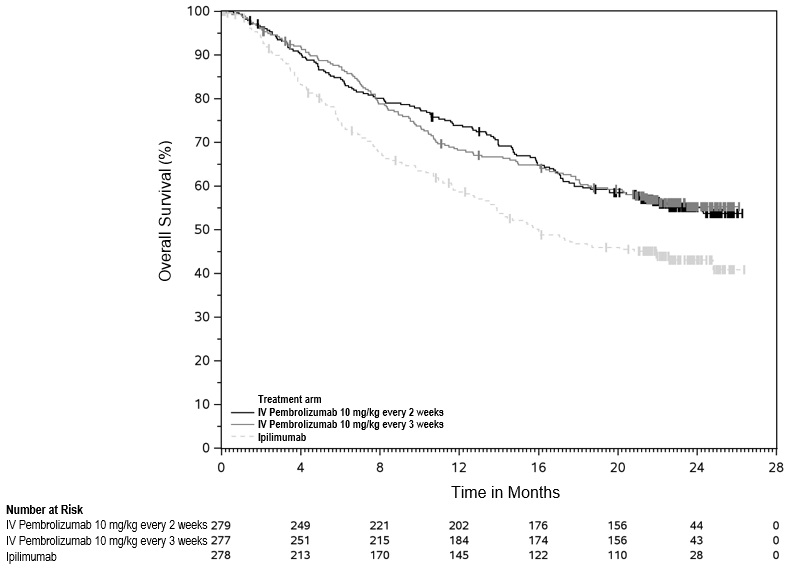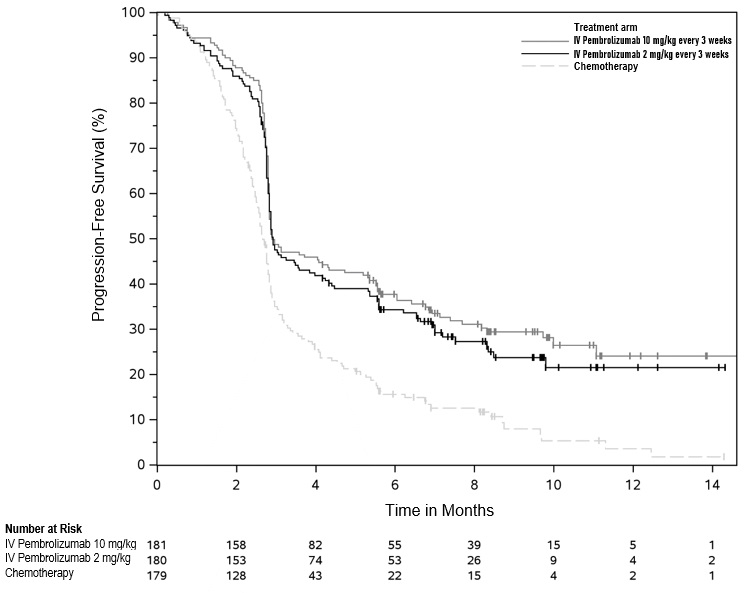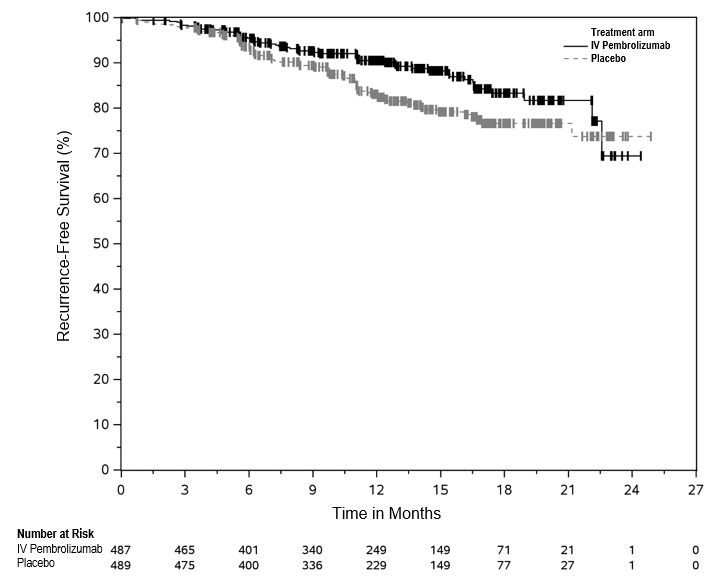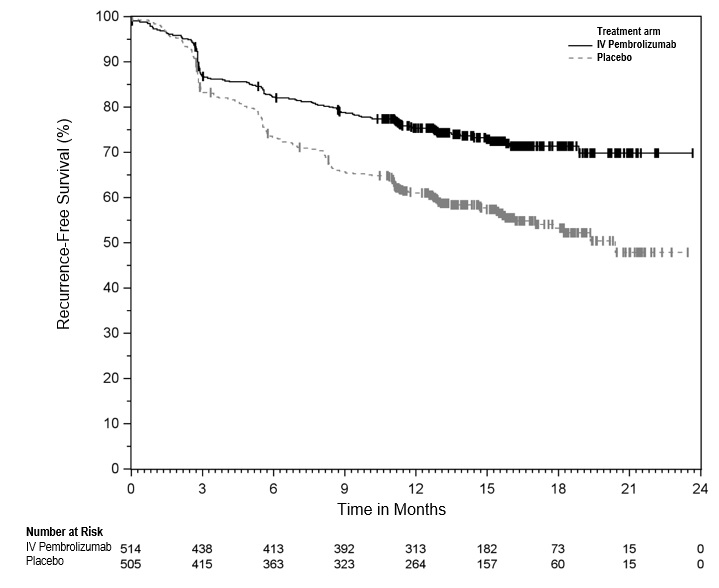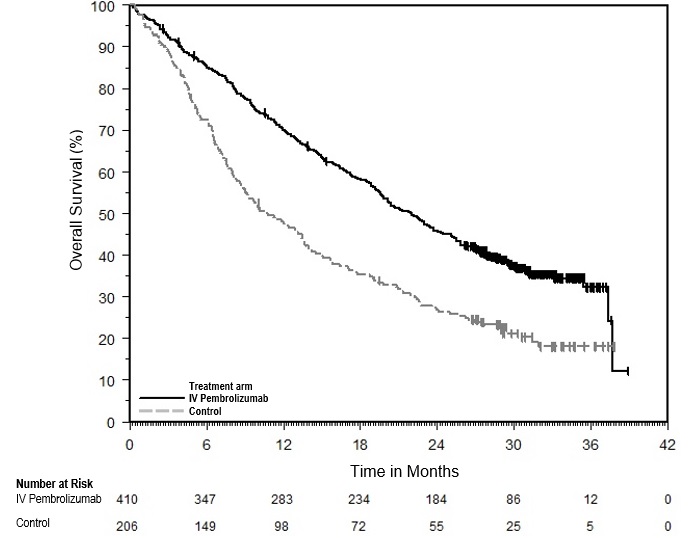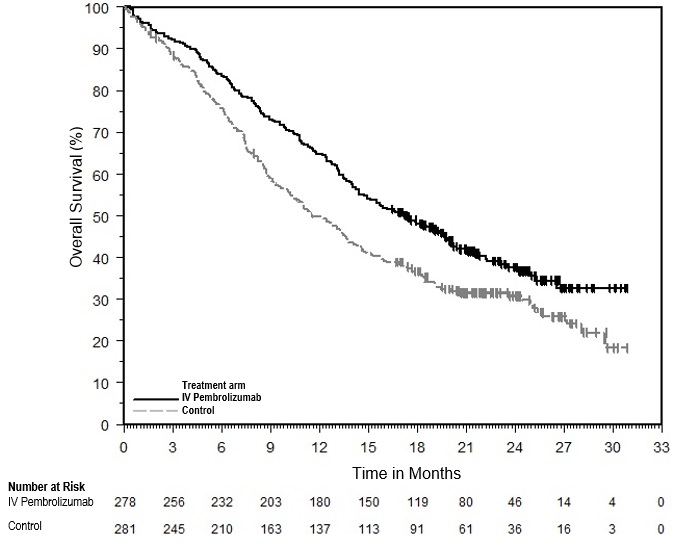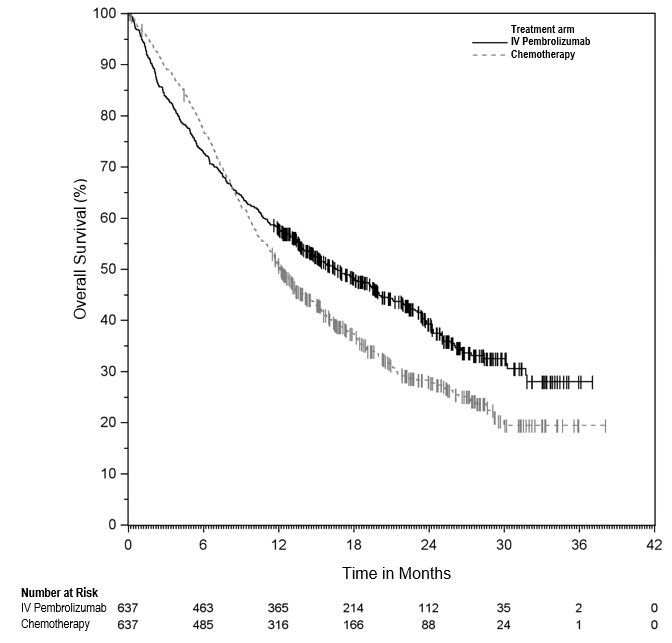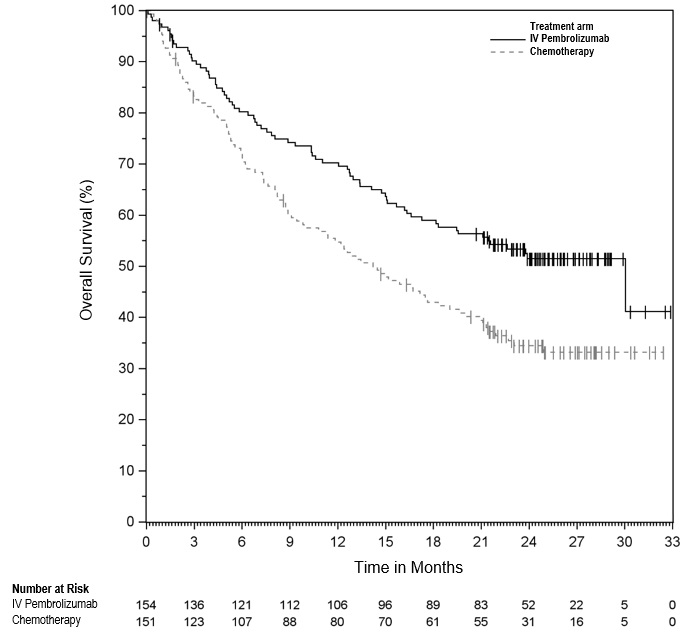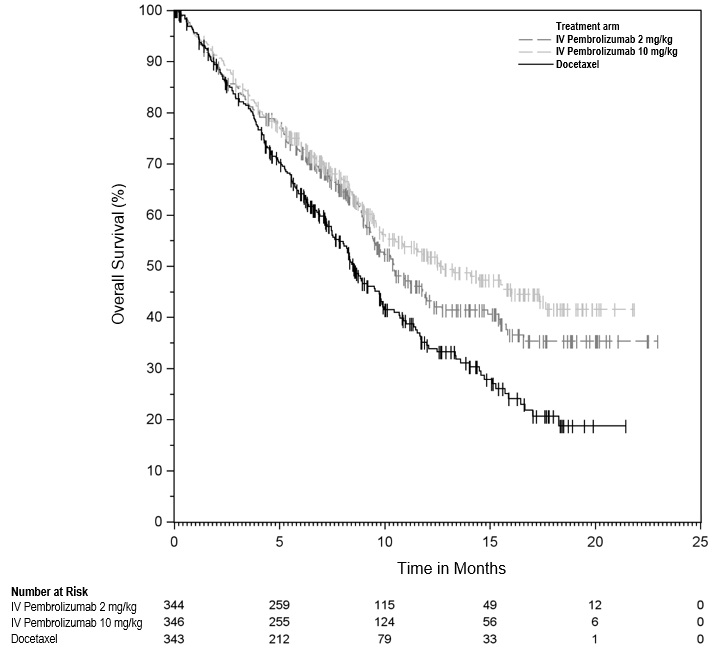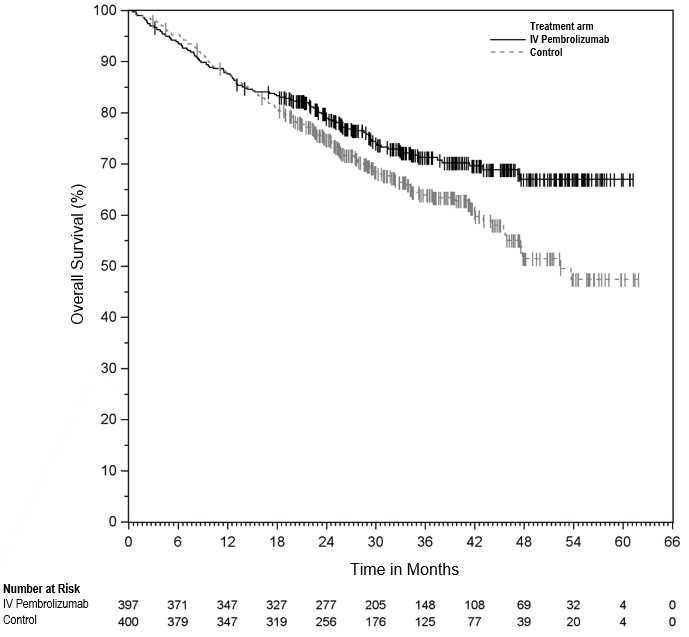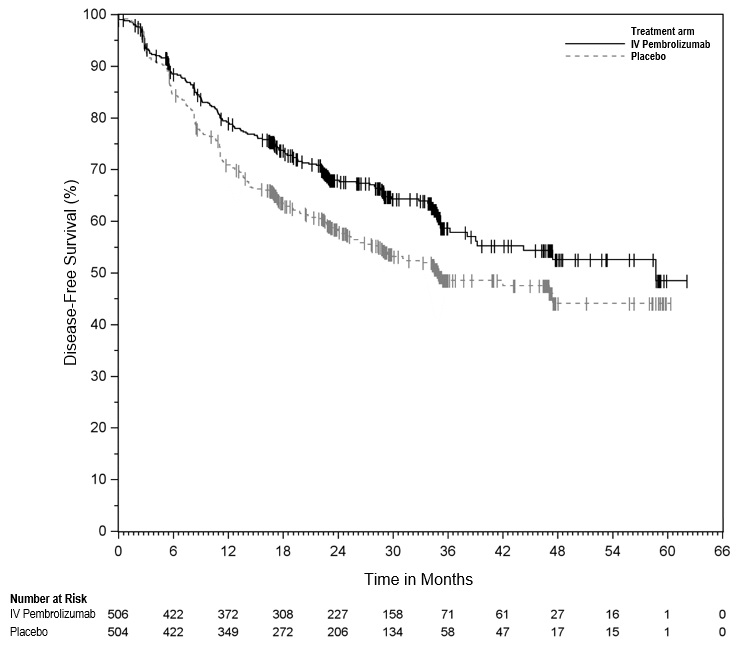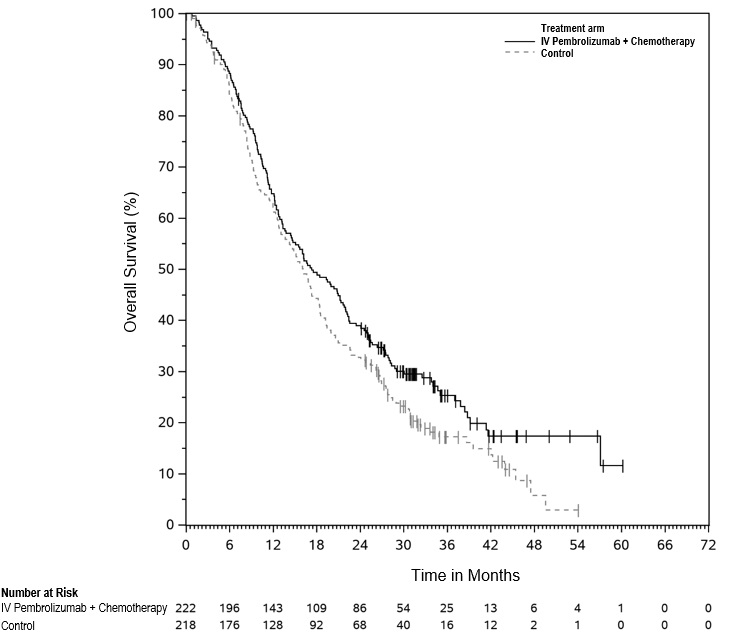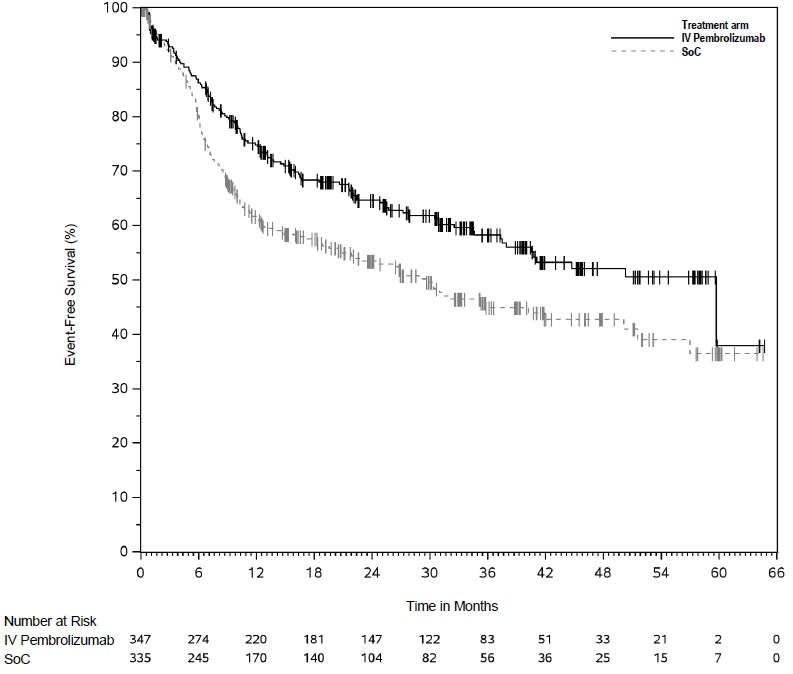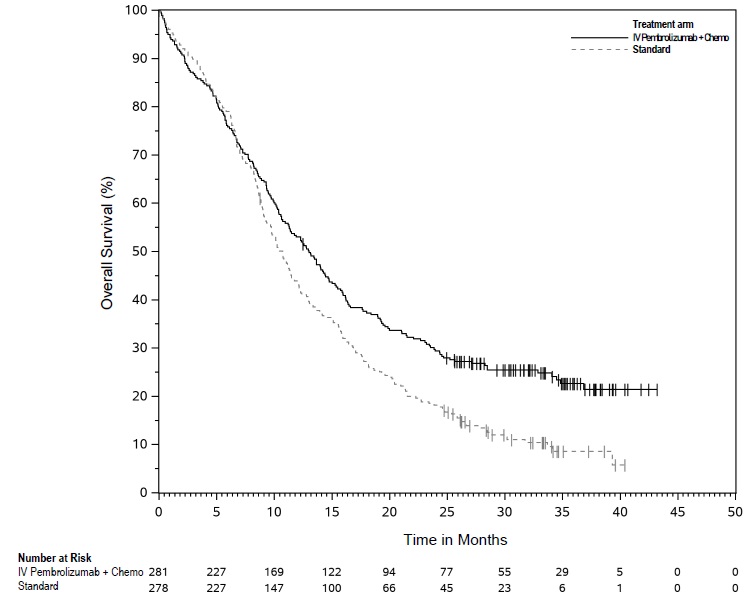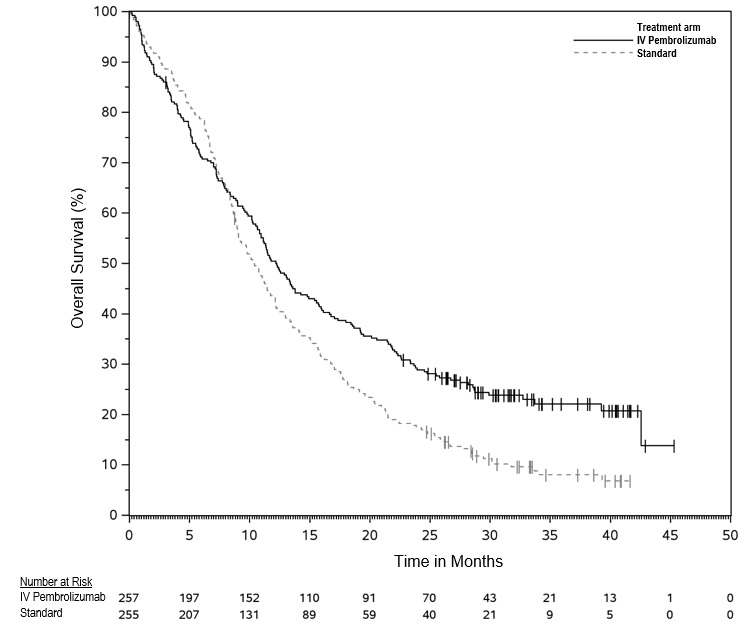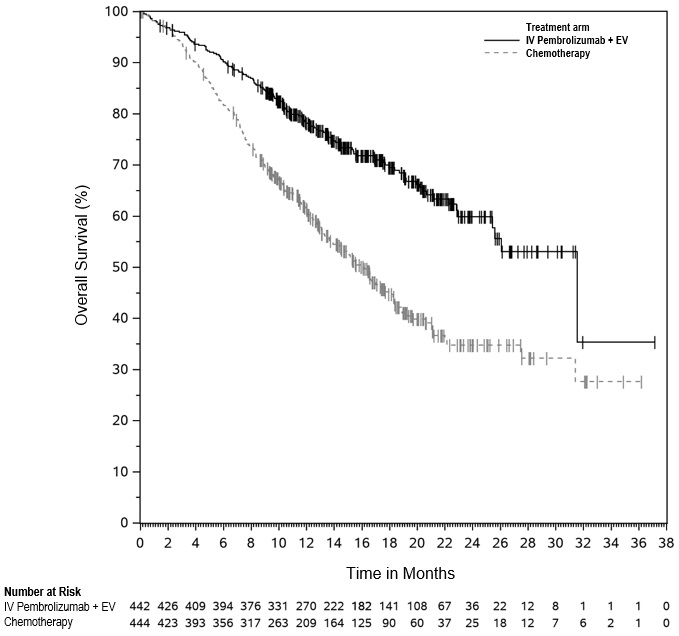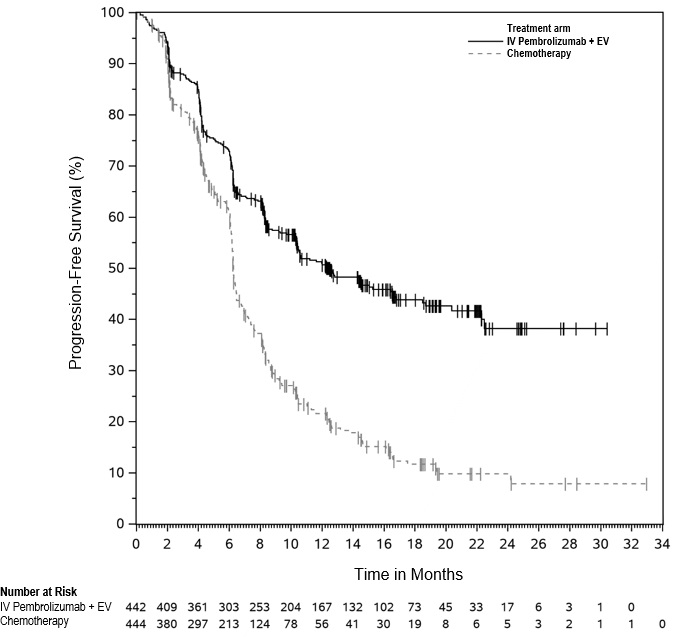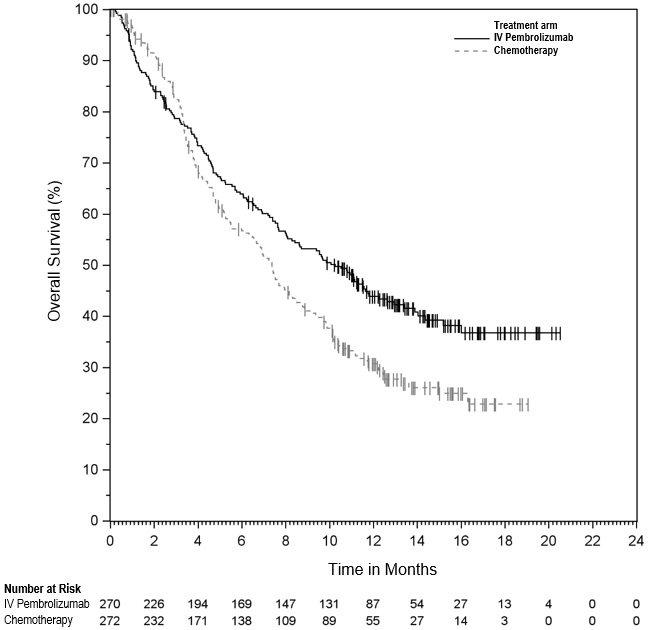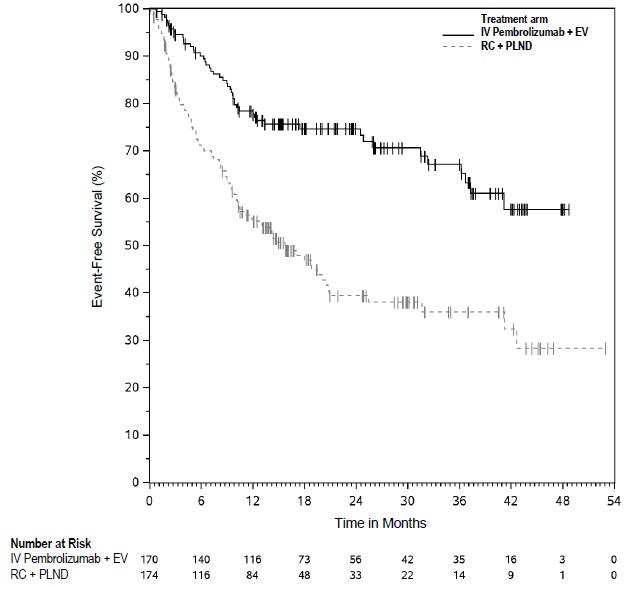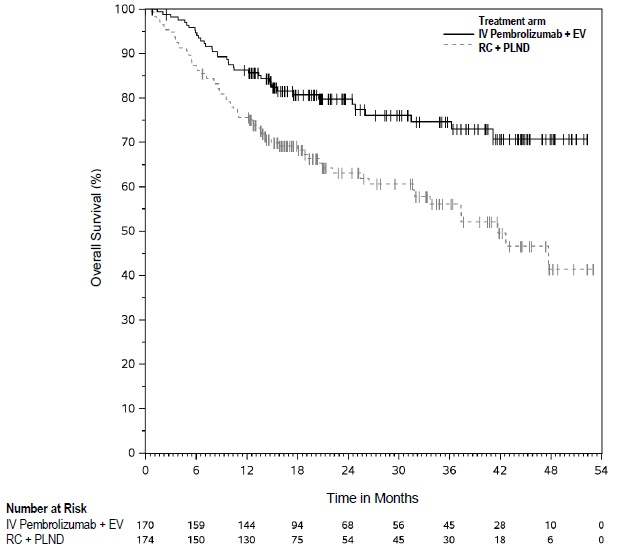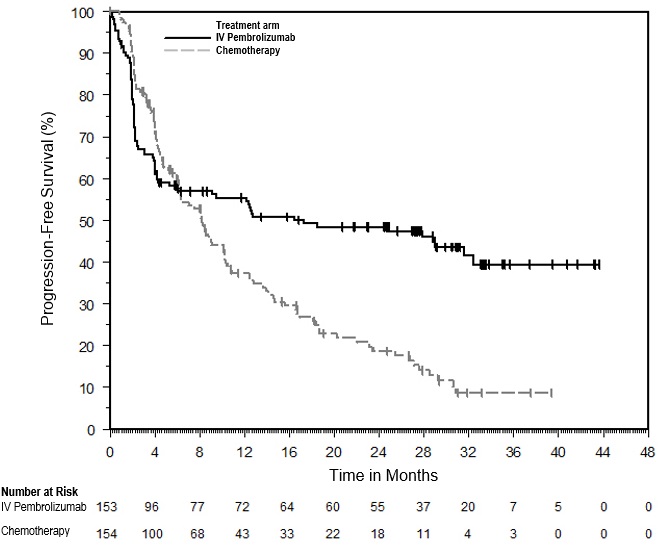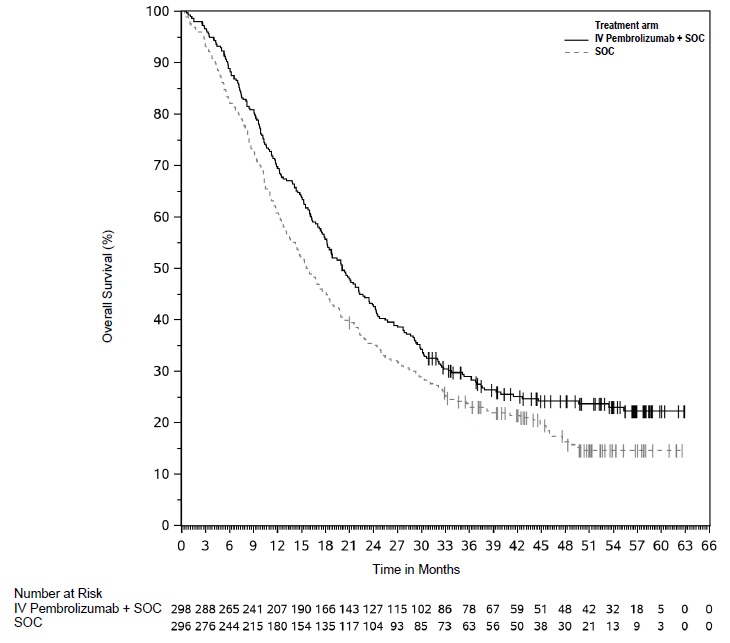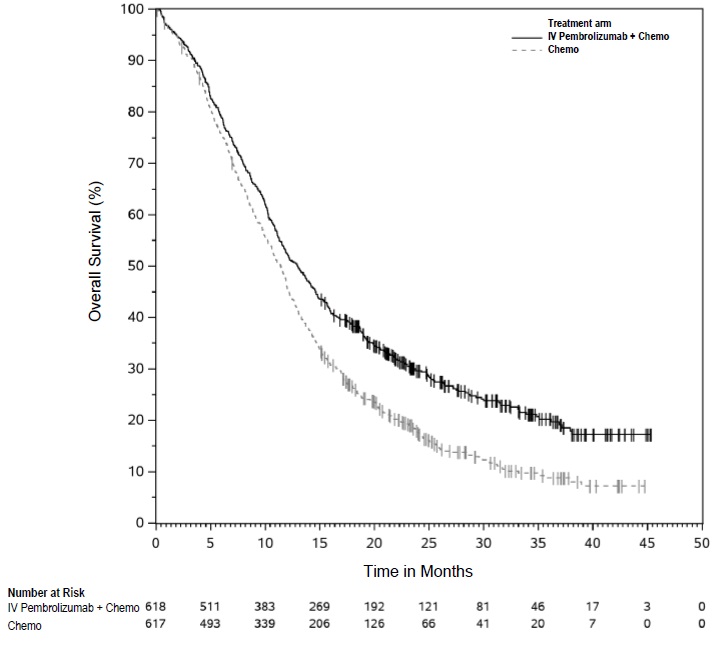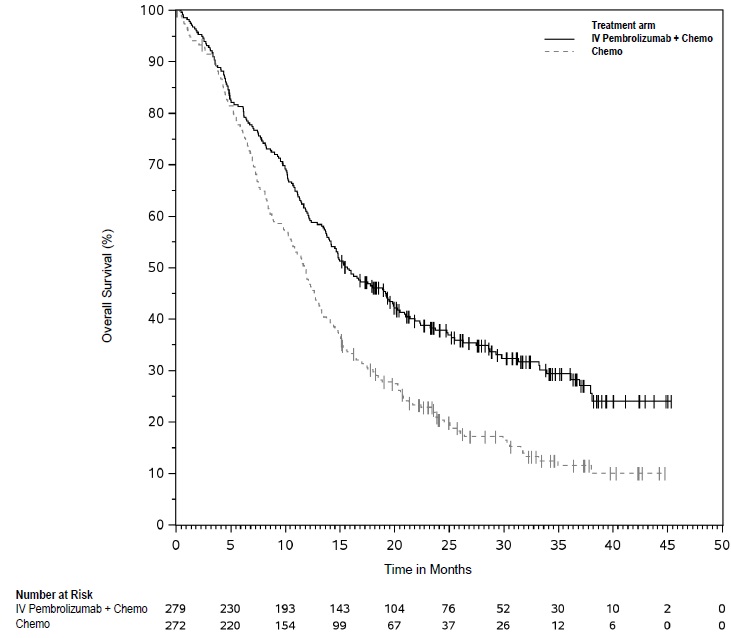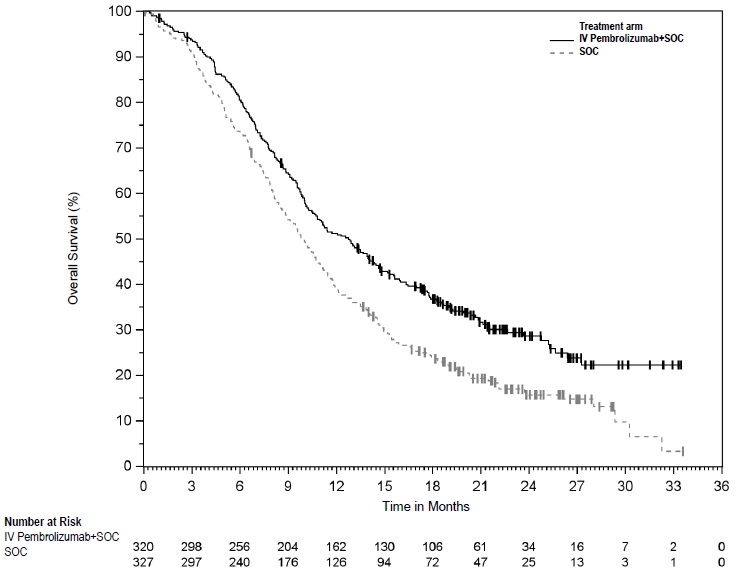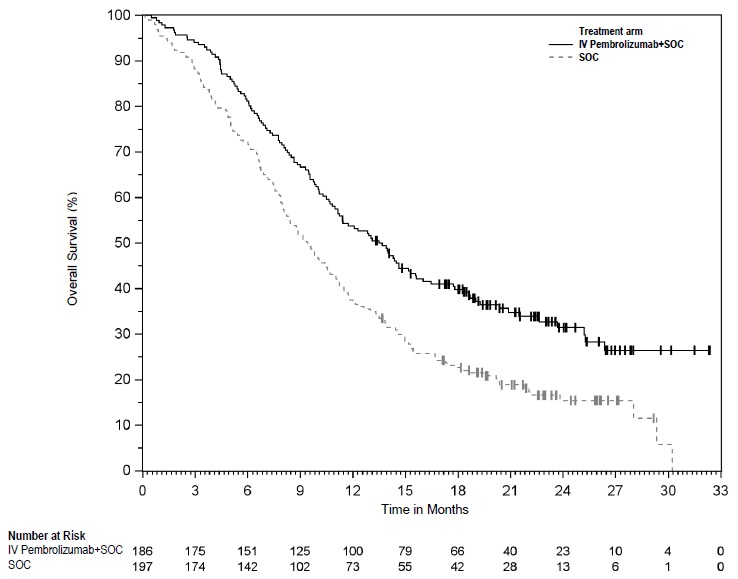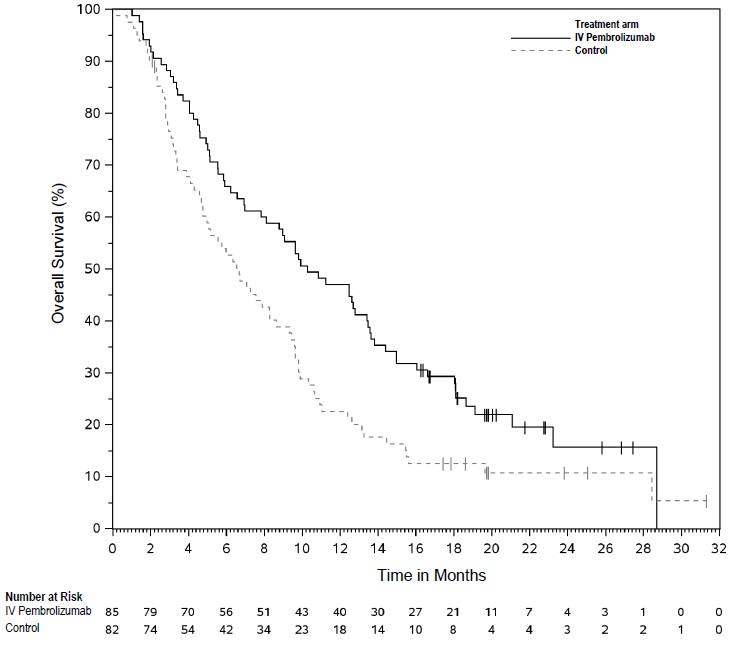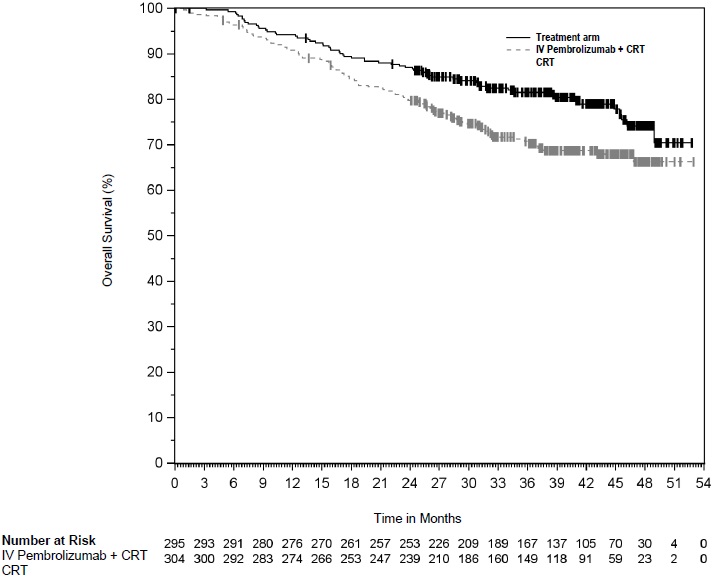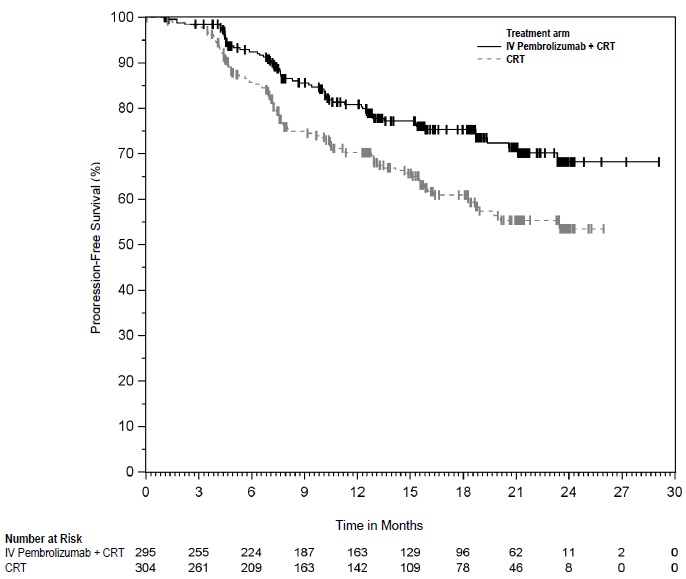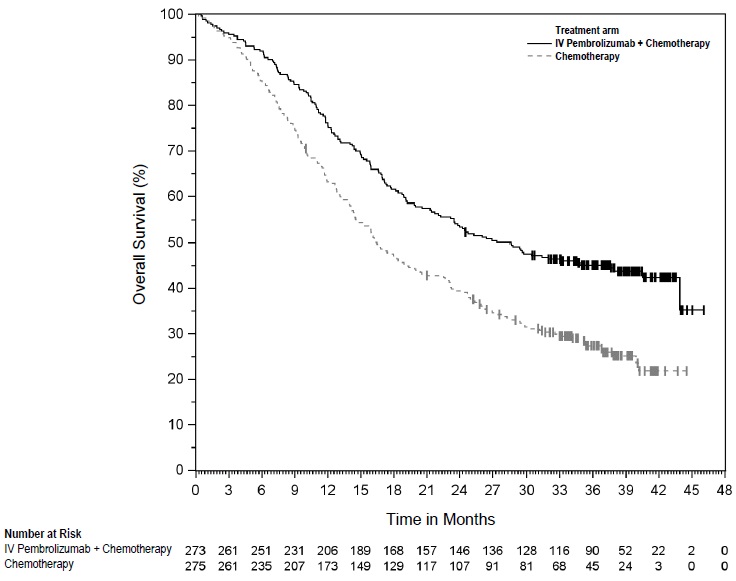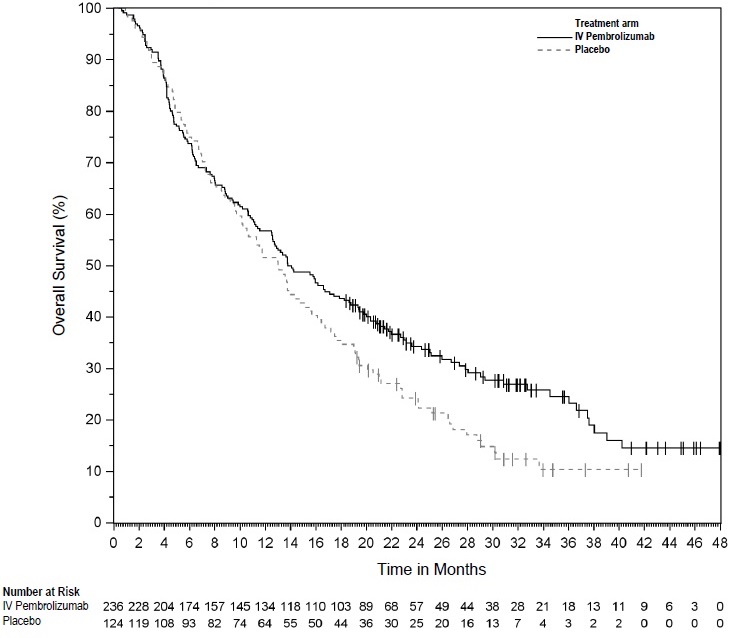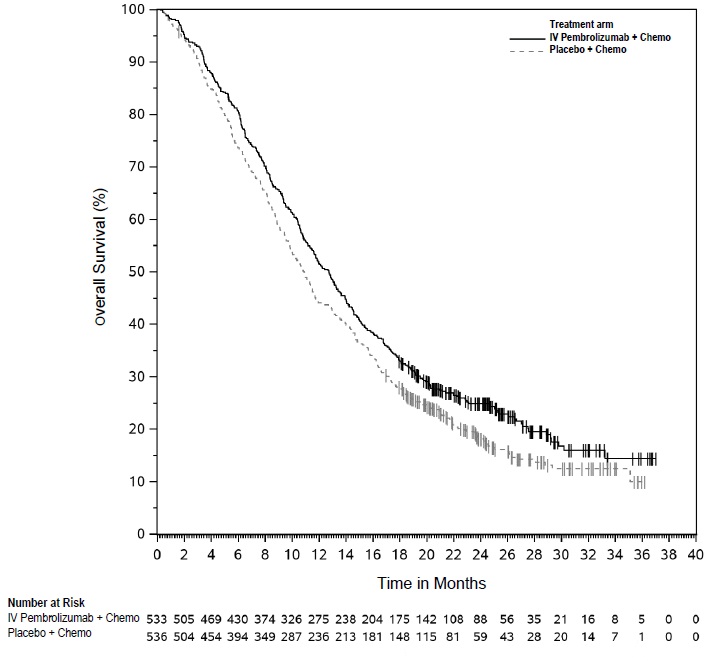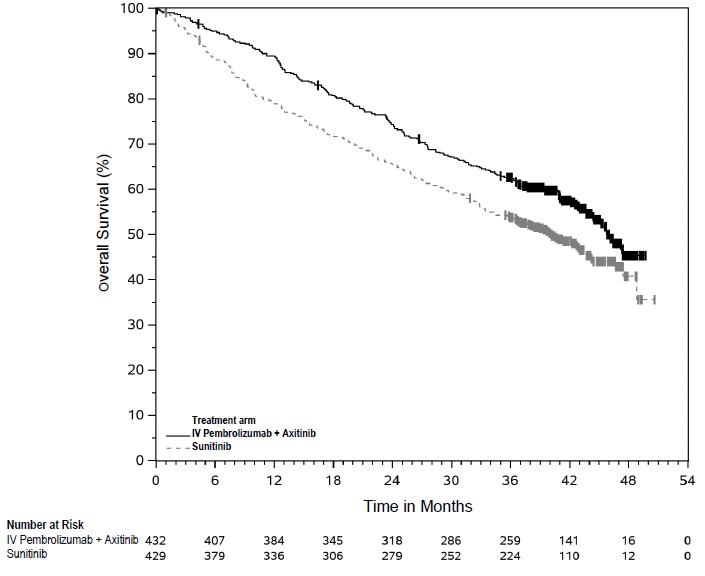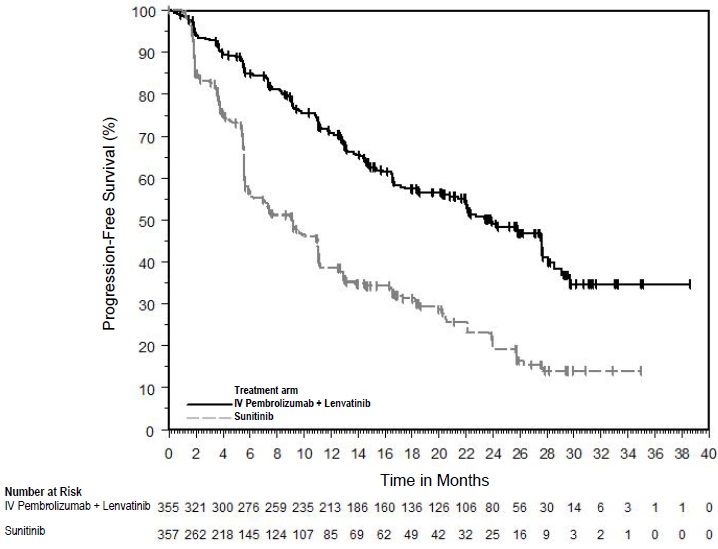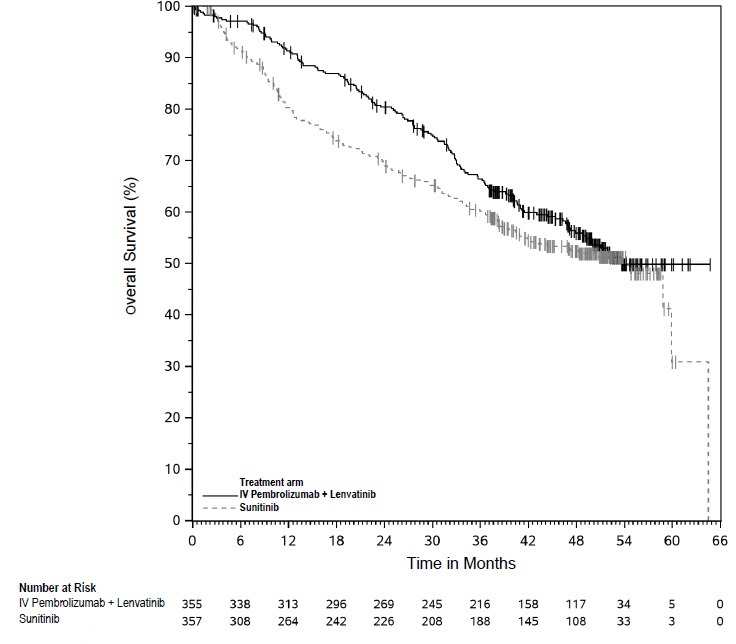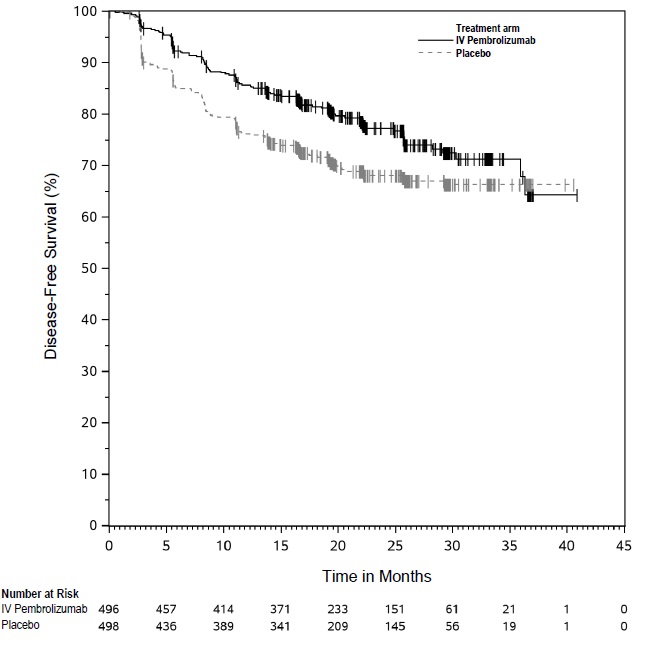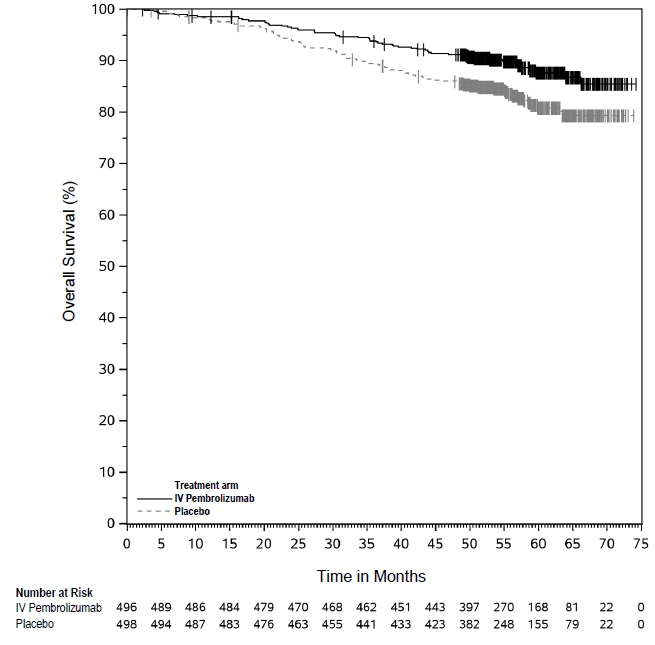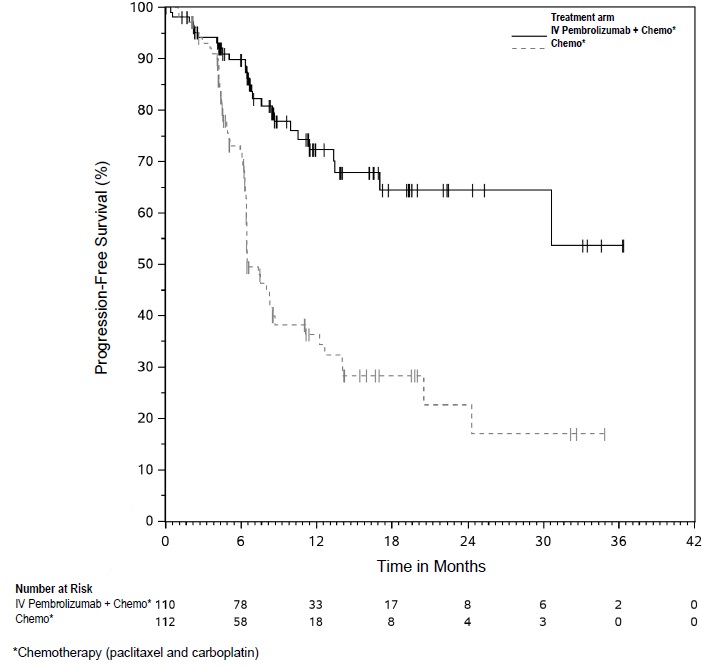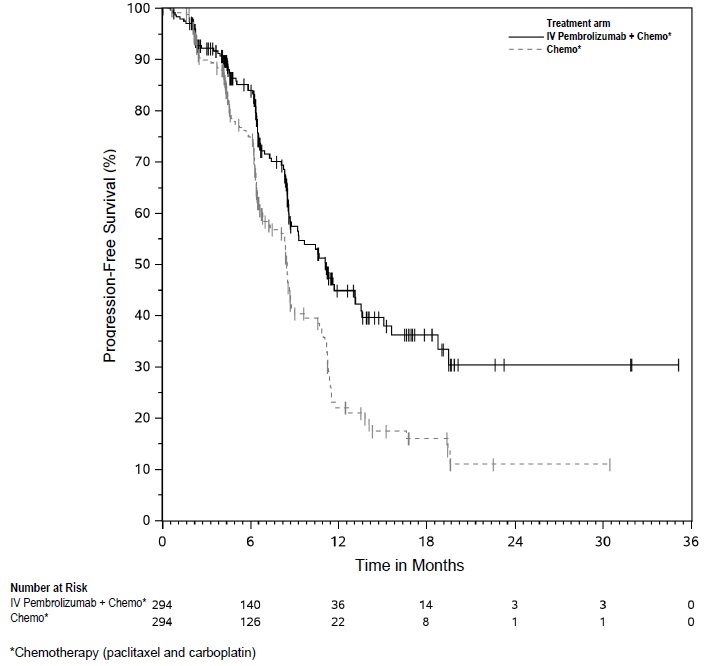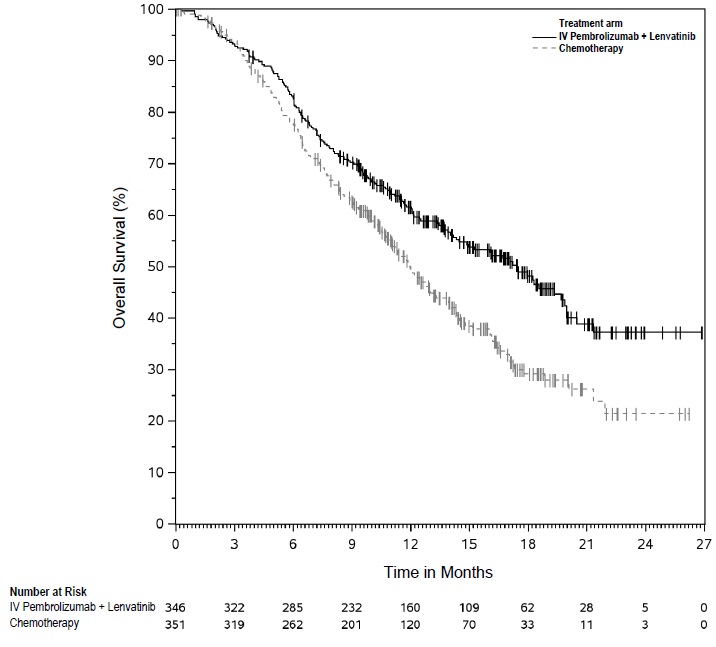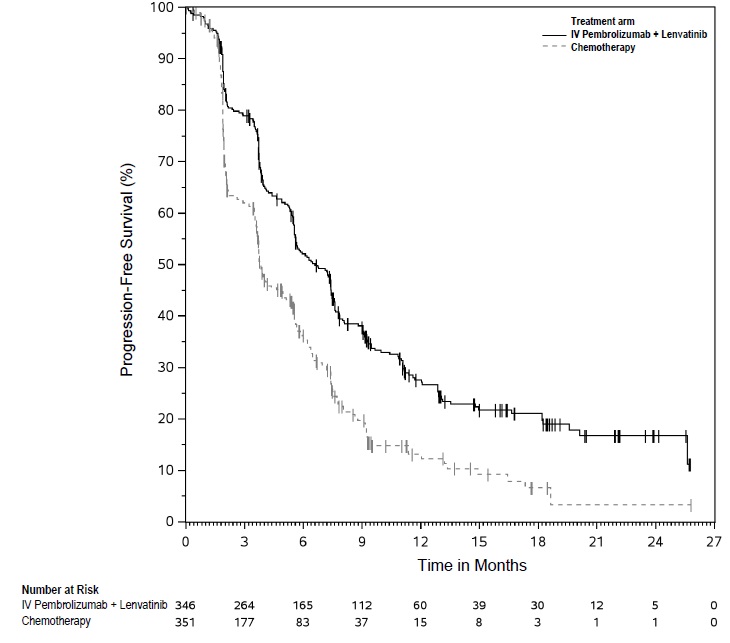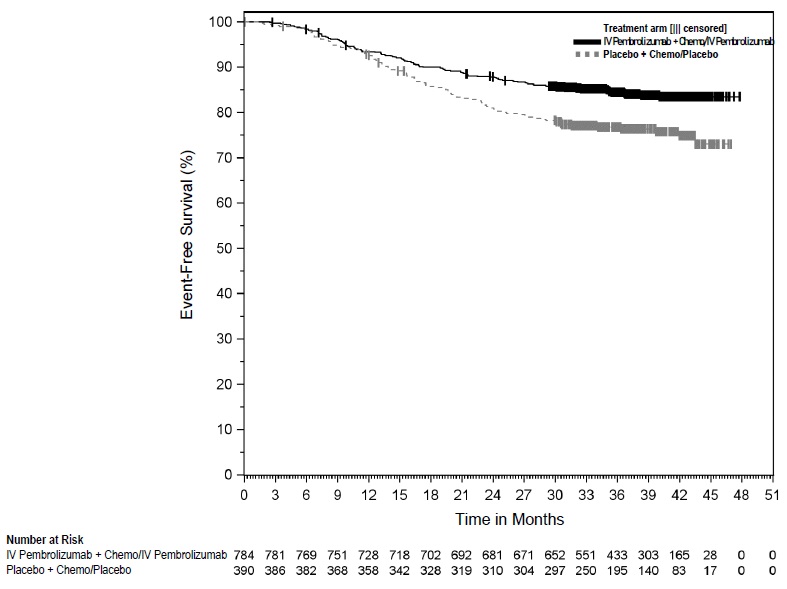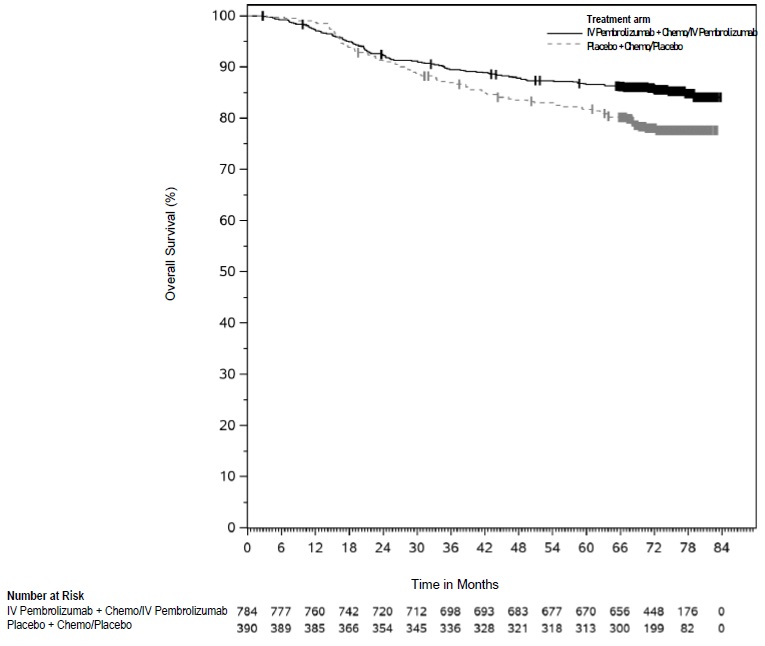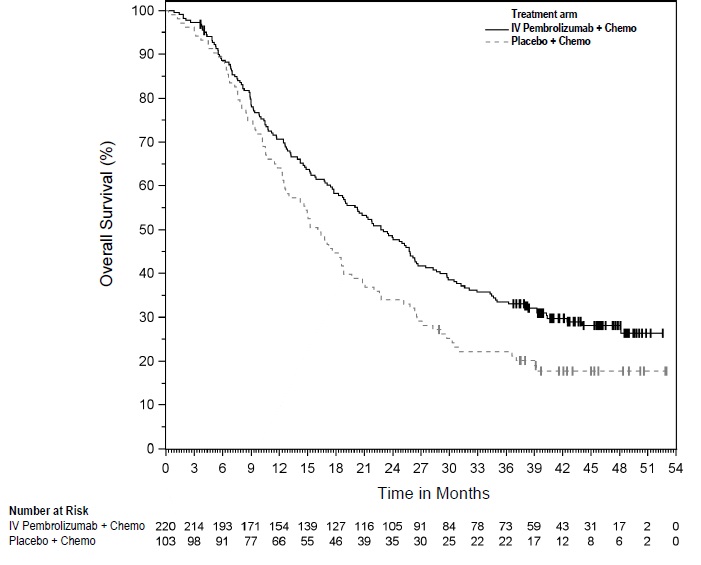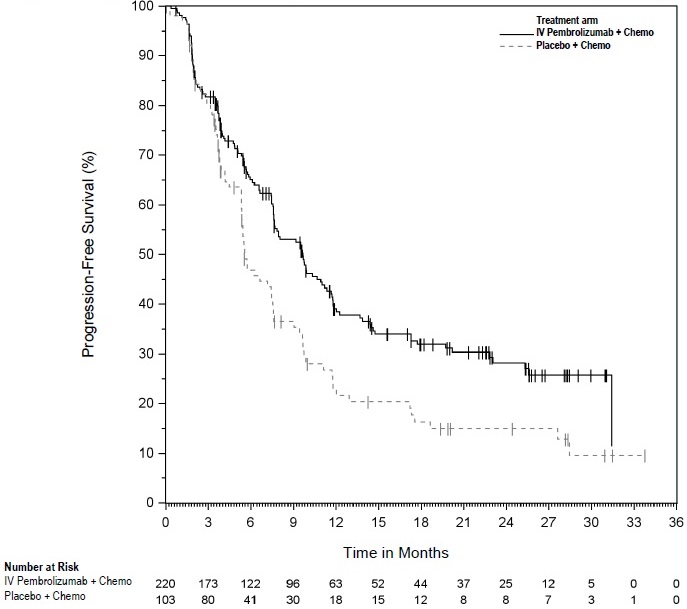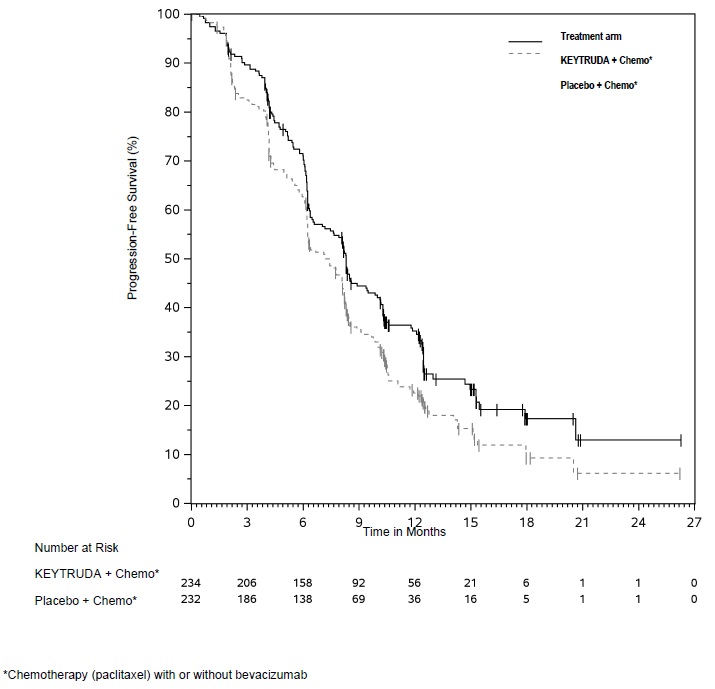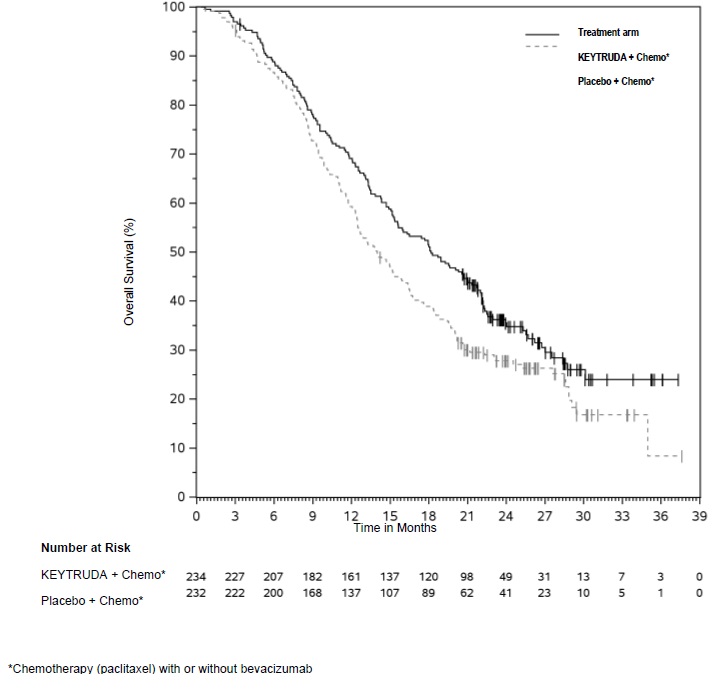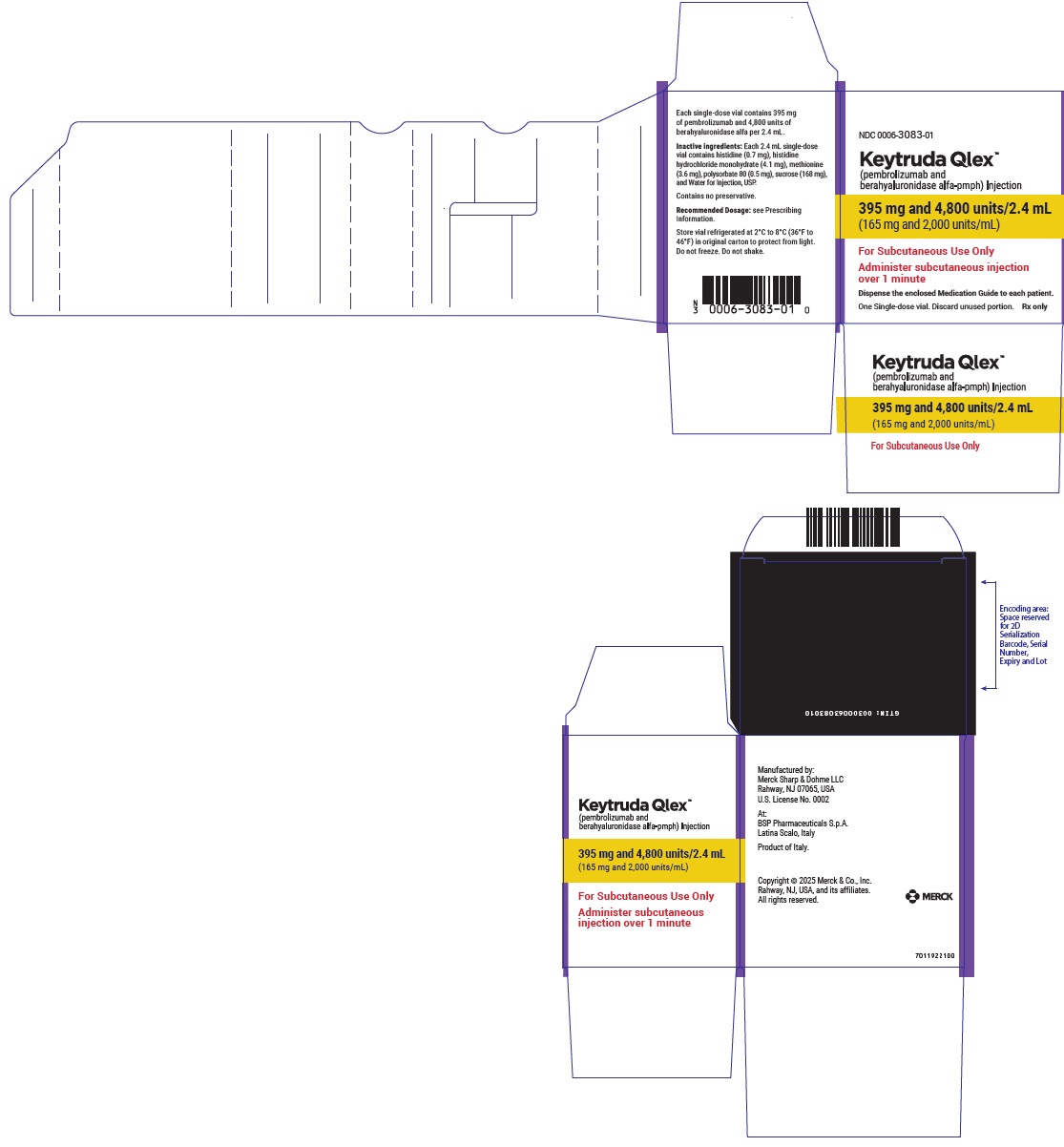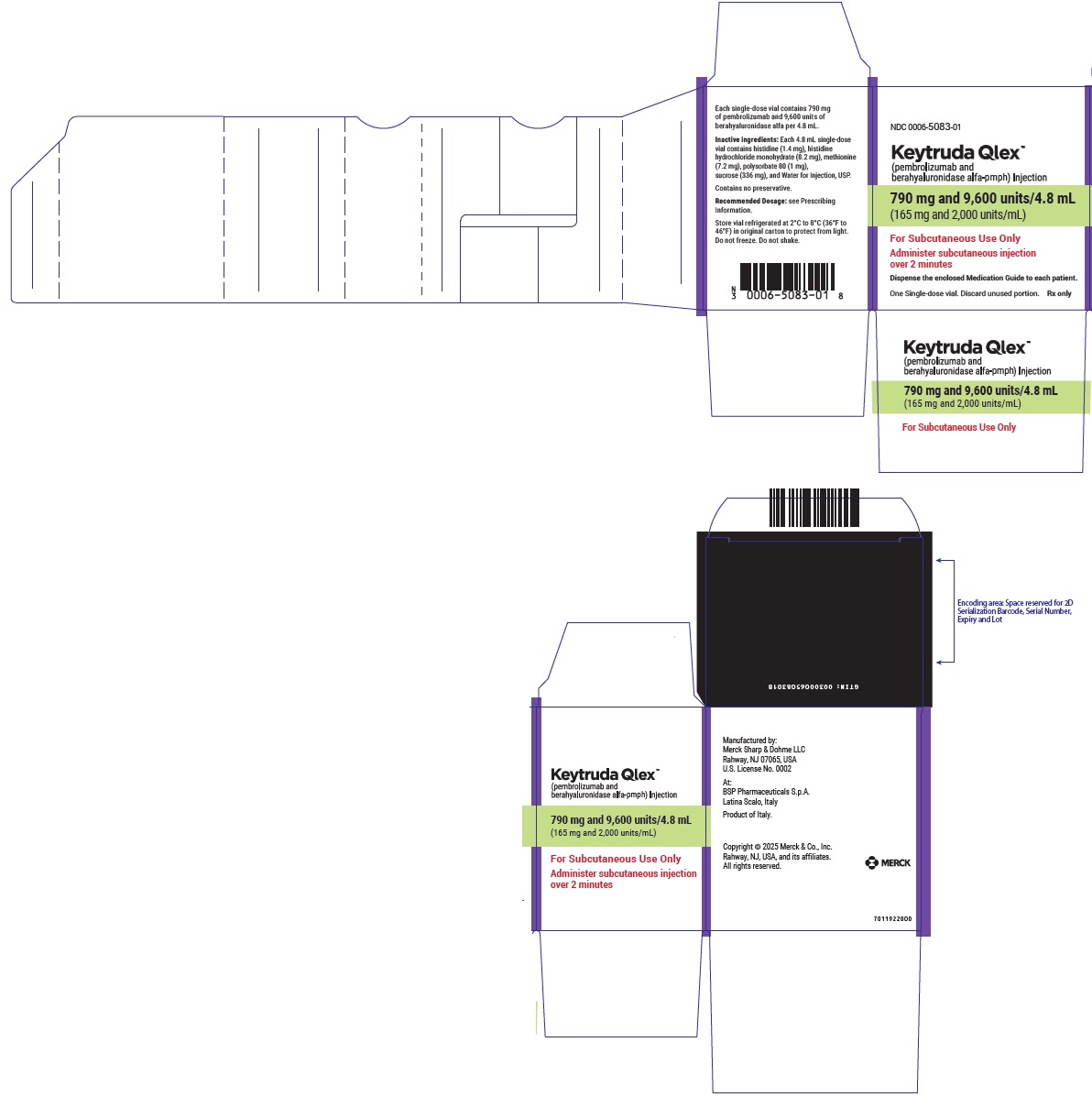 DRUG LABEL: KEYTRUDA QLEX
NDC: 0006-5083 | Form: INJECTION, SOLUTION
Manufacturer: Merck Sharp & Dohme LLC
Category: prescription | Type: HUMAN PRESCRIPTION DRUG LABEL
Date: 20260210

ACTIVE INGREDIENTS: PEMBROLIZUMAB 165 mg/1 mL; BERAHYALURONIDASE ALFA 2000 U/1 mL
INACTIVE INGREDIENTS: HISTIDINE 0.3 mg/1 mL; HISTIDINE MONOHYDROCHLORIDE MONOHYDRATE 1.7 mg/1 mL; METHIONINE 1.5 mg/1 mL; SUCROSE 70 mg/1 mL; POLYSORBATE 80 0.2 mg/1 mL; WATER

HIGHLIGHTS OF PRESCRIBING INFORMATION

These highlights do not include all the information needed to use KEYTRUDA QLEX safely and effectively. See full prescribing information for KEYTRUDA QLEX.
KEYTRUDA QLEX™ (pembrolizumab and berahyaluronidase alfa-pmph) injection, for subcutaneous use
Initial U.S. Approval: 2025

RECENT MAJOR CHANGES

Indications and Usage (1) | 02/2026
Dosage and Administration (2) | 02/2026

1 INDICATIONS AND USAGE

KEYTRUDA QLEX is a combination of pembrolizumab, a programmed death receptor-1 (PD-1)-blocking antibody, and berahyaluronidase alfa, an endoglycosidase, indicated:

Melanoma

- for the treatment of adult patients with unresectable or metastatic melanoma. (1.1)
- for the adjuvant treatment of adult and pediatric patients 12 years and older with Stage IIB, IIC, or III melanoma following complete resection. (1.1)

Non-Small Cell Lung Cancer (NSCLC)

- in combination with pemetrexed and platinum chemotherapy, as first-line treatment of adult patients with metastatic nonsquamous NSCLC, with no EGFR or ALK genomic tumor aberrations. (1.2)
- in combination with carboplatin and either paclitaxel or paclitaxel protein-bound, as first-line treatment of adult patients with metastatic squamous NSCLC. (1.2)
- as a single agent for the first-line treatment of adult patients with NSCLC expressing PD-L1 [Tumor Proportion Score (TPS) ≥1%] as determined by an FDA-authorized test, with no EGFR or ALK genomic tumor aberrations, and is:
  - Stage III where patients are not candidates for surgical resection or definitive chemoradiation, or
  - metastatic. (1.2, 2.1)
- as a single agent for the treatment of adult patients with metastatic NSCLC whose tumors express PD-L1 (TPS ≥1%) as determined by an FDA-authorized test, with disease progression on or after platinum-containing chemotherapy. Patients with EGFR or ALK genomic tumor aberrations should have disease progression on FDA-approved therapy for these aberrations prior to receiving KEYTRUDA QLEX. (1.2, 2.1)
- for the treatment of adult patients with resectable (tumors ≥4 cm or node positive) NSCLC in combination with platinum-containing chemotherapy as neoadjuvant treatment, and then continued as a single agent as adjuvant treatment after surgery. (1.2)
- as a single agent, for adjuvant treatment following resection and platinum-based chemotherapy for adult patients with Stage IB (T2a ≥4 cm), II, or IIIA NSCLC. (1.2)

Malignant Pleural Mesothelioma (MPM)

- in combination with pemetrexed and platinum chemotherapy, as first-line treatment of adult patients with unresectable advanced or metastatic MPM. (1.3)

Head and Neck Squamous Cell Cancer (HNSCC)

- for the treatment of adult patients with resectable locally advanced HNSCC whose tumors express PD-L1 [Combined Positive Score (CPS) ≥1] as determined by an FDA-authorized test, as a single agent as neoadjuvant treatment, continued as adjuvant treatment in combination with radiotherapy (RT) with or without cisplatin and then as a single agent. (1.4)
- in combination with platinum and FU for the first-line treatment of adult patients with metastatic or with unresectable, recurrent HNSCC. (1.4)
- as a single agent for the first-line treatment of adult patients with metastatic or with unresectable, recurrent HNSCC whose tumors express PD-L1 [Combined Positive Score (CPS) ≥1] as determined by an FDA-authorized test. (1.4, 2.1)
- as a single agent for the treatment of adult patients with recurrent or metastatic HNSCC with disease progression on or after platinum-containing chemotherapy. (1.4)

Urothelial Cancer

- in combination with enfortumab vedotin, for the treatment of adult patients with locally advanced or metastatic urothelial cancer. (1.5)
- as a single agent for the treatment of adult patients with locally advanced or metastatic urothelial carcinoma who:
  - are not eligible for any platinum-containing chemotherapy, or
  - who have disease progression during or following platinum-containing chemotherapy or within 12 months of neoadjuvant or adjuvant treatment with platinum-containing chemotherapy. (1.5)
- in combination with enfortumab vedotin, as neoadjuvant treatment and then continued after cystectomy as adjuvant treatment of adult patients with muscle invasive bladder cancer (MIBC) who are ineligible for cisplatin-containing chemotherapy. (1.5)
- as a single agent for the treatment of adult patients with Bacillus Calmette-Guerin (BCG)-unresponsive, high-risk, non-muscle invasive bladder cancer (NMIBC) with carcinoma in situ (CIS) with or without papillary tumors who are ineligible for or have elected not to undergo cystectomy. (1.5)

Microsatellite Instability-High or Mismatch Repair Deficient Cancer

- for the treatment of adult and pediatric patients 12 years and older with unresectable or metastatic microsatellite instability-high (MSI-H) or mismatch repair deficient (dMMR) solid tumors, as determined by an FDA-authorized test, that have progressed following prior treatment and who have no satisfactory alternative treatment options. (1.6, 2.1)

Microsatellite Instability-High or Mismatch Repair Deficient Colorectal Cancer (CRC)

- for the treatment of adult patients with unresectable or metastatic MSI-H or dMMR colorectal cancer (CRC) as determined by an FDA-authorized test. (1.7, 2.1)

Gastric Cancer

- in combination with trastuzumab, fluoropyrimidine- and platinum-containing chemotherapy, for the first-line treatment of adults with locally advanced unresectable or metastatic HER2-positive gastric or gastroesophageal junction (GEJ) adenocarcinoma whose tumors express PD-L1 (CPS ≥1) as determined by an FDA-authorized test. (1.8)
- in combination with fluoropyrimidine- and platinum-containing chemotherapy, for the first-line treatment of adults with locally advanced unresectable or metastatic HER2-negative gastric or gastroesophageal junction (GEJ) adenocarcinoma whose tumors express PD-L1 (CPS ≥1) as determined by an FDA-authorized test. (1.8)

Esophageal Cancer

- for the treatment of adult patients with locally advanced or metastatic esophageal or gastroesophageal junction (GEJ) (tumors with epicenter 1 to 5 centimeters above the GEJ) carcinoma that is not amenable to surgical resection or definitive chemoradiation either:
  - in combination with platinum- and fluoropyrimidine-based chemotherapy for patients whose tumors express PD-L1 (CPS ≥1), or
  - as a single agent after one or more prior lines of systemic therapy for patients with tumors of squamous cell histology that express PD-L1 (CPS ≥10) as determined by an FDA-authorized test. (1.9, 2.1)

Cervical Cancer

- in combination with chemoradiotherapy, for the treatment of adult patients with locally advanced cervical cancer involving the lower third of the vagina, with or without extension to pelvic sidewall, or hydronephrosis/non-functioning kidney, or spread to adjacent pelvic organs (FIGO 2014 Stage III-IVA). (1.10)
- in combination with chemotherapy, with or without bevacizumab, for the treatment of adult patients with persistent, recurrent, or metastatic cervical cancer whose tumors express PD-L1 (CPS ≥1) as determined by an FDA-authorized test. (1.10, 2.1)
- as a single agent for the treatment of adult patients with recurrent or metastatic cervical cancer with disease progression on or after chemotherapy whose tumors express PD-L1 (CPS ≥1) as determined by an FDA-authorized test. (1.10, 2.1)

Hepatocellular Carcinoma (HCC)

- for the treatment of adult patients with HCC secondary to hepatitis B who have received prior systemic therapy other than a PD-1/PD-L1-containing regimen. (1.11)

Biliary Tract Cancer (BTC)

- in combination with gemcitabine and cisplatin, for the treatment of adult patients with locally advanced unresectable or metastatic biliary tract cancer. (1.12)

Merkel Cell Carcinoma (MCC)

- for the treatment of adult and pediatric patients 12 years and older with recurrent locally advanced or metastatic Merkel cell carcinoma. (1.13)

Renal Cell Carcinoma (RCC)

- in combination with axitinib, for the first-line treatment of adult patients with advanced RCC. (1.14)
- in combination with lenvatinib, for the first-line treatment of adult patients with advanced RCC. (1.14)
- for the adjuvant treatment of adult patients with RCC at intermediate-high or high risk of recurrence following nephrectomy, or following nephrectomy and resection of metastatic lesions. (1.14)

Endometrial Carcinoma

- in combination with carboplatin and paclitaxel, followed by KEYTRUDA QLEX as a single agent, for the treatment of adult patients with primary advanced or recurrent endometrial carcinoma. (1.15)
- in combination with lenvatinib, for the treatment of adult patients with advanced endometrial carcinoma that is mismatch repair proficient (pMMR) or not MSI-H as determined by an FDA-authorized test, who have disease progression following prior systemic therapy in any setting and are not candidates for curative surgery or radiation. (1.15, 2.1)
- as a single agent, for the treatment of adult patients with advanced endometrial carcinoma that is MSI-H or dMMR, as determined by an FDA-authorized test, who have disease progression following prior systemic therapy in any setting and are not candidates for curative surgery or radiation. (1.15, 2.1)

Tumor Mutational Burden-High (TMB-H) Cancer

- for the treatment of adult and pediatric patients 12 years and older with unresectable or metastatic tumor mutational burden-high (TMB-H) [≥10 mutations/megabase (mut/Mb)] solid tumors, as determined by an FDA-authorized test, that have progressed following prior treatment and who have no satisfactory alternative treatment options.^1 (1.16, 2.1)
- Limitations of Use: The safety and effectiveness of KEYTRUDA QLEX in pediatric patients 12 years and older with TMB-H central nervous system cancers have not been established.

Cutaneous Squamous Cell Carcinoma (cSCC)

- for the treatment of adult patients with recurrent or metastatic cSCC or locally advanced cSCC that is not curable by surgery or radiation. (1.17)

Triple-Negative Breast Cancer (TNBC)

- for the treatment of adult patients with high-risk early-stage TNBC in combination with chemotherapy as neoadjuvant treatment, and then continued as a single agent as adjuvant treatment after surgery. (1.18)
- in combination with chemotherapy, for the treatment of adult patients with locally recurrent unresectable or metastatic TNBC whose tumors express PD-L1 (CPS ≥10) as determined by an FDA-authorized test. (1.18, 2.1)

Ovarian Cancer

- in combination with paclitaxel, with or without bevacizumab, is indicated for the treatment of adult patients with platinum-resistant epithelial ovarian, fallopian tube, or primary peritoneal carcinoma whose tumors express PD-L1 (CPS ≥1) as determined by an FDA-authorized test, and who have received one or two prior systemic treatment regimens. (1.19, 2.1)

^1 This indication is approved under accelerated approval based on tumor response rate and durability of response. Continued approval for this indication may be contingent upon verification and description of clinical benefit in the confirmatory trials.

2 DOSAGE AND ADMINISTRATION

KEYTRUDA QLEX has different recommended dosage and administration than intravenous pembrolizumab. (2.2)

- KEYTRUDA QLEX is for subcutaneous use in the thigh or abdomen only. (2.2)
- Do not administer KEYTRUDA QLEX intravenously. (2.2)
- KEYTRUDA QLEX must be administered by a healthcare provider. (2.2)

The recommended dose for adults and pediatric patients 12 years and older who weigh greater than 40 kg is:

- Every 3-week dosing (395 mg/4,800 units): Inject 2.4 mL subcutaneously in the abdomen or thigh over 1 minute. (2.3)
- Every 6-week dosing (790 mg/9,600 units): Inject 4.8 mL subcutaneously in the abdomen or thigh over 2 minutes. (2.3)
- For RCC, administer KEYTRUDA QLEX as a single agent in the adjuvant setting, or in the advanced setting with either:
  - axitinib 5 mg orally twice daily or
  - lenvatinib 20 mg orally once daily. (2.3)
- For Endometrial Carcinoma, administer KEYTRUDA QLEX:
  - in combination with carboplatin and paclitaxel regardless of MMR or MSI status, or
  - in combination with lenvatinib 20 mg orally once daily for pMMR or not MSI-H tumors, or
  - as a single agent for MSI-H or dMMR tumors. (2.3)

- See Full Prescribing Information for dosage modifications for adverse reactions and preparation and administration instructions. (2.4, 2.5)

3 DOSAGE FORMS AND STRENGTHS

Injection: (3)

- 395 mg pembrolizumab and 4,800 units berahyaluronidase alfa per 2.4 mL (165 mg/2,000 units per mL) in a single-dose vial
- 790 mg pembrolizumab and 9,600 units berahyaluronidase alfa per 4.8 mL (165 mg/2,000 units per mL) in a single-dose vial

4 CONTRAINDICATIONS

KEYTRUDA QLEX is contraindicated in patients with known hypersensitivity to berahyaluronidase alfa, hyaluronidase or to any of its excipients. (4)

5 WARNINGS AND PRECAUTIONS

- Immune-Mediated Adverse Reactions (5.1)
  - Immune-mediated adverse reactions, which may be severe or fatal, can occur in any organ system or tissue, including the following: immune-mediated pneumonitis, immune-mediated colitis, immune-mediated hepatitis, immune-mediated endocrinopathies, immune-mediated nephritis with renal dysfunction, immune-mediated dermatologic adverse reactions, and solid organ transplant rejection.
  - Monitor for early identification and management. Evaluate liver enzymes, creatinine, and thyroid function at baseline and periodically during treatment.
  - Withhold or permanently discontinue based on severity and type of reaction.
- Hypersensitivity and Administration-Related Reactions: Interrupt injection and resume upon symptom resolution, or permanently discontinue KEYTRUDA QLEX based on the severity of reaction. (5.2)
- Complications of Allogeneic HSCT: Fatal and other serious complications can occur in patients who receive allogeneic HSCT before or after being treated with a PD-1/PD-L1 blocking antibody. (5.3)
- Treatment of patients with multiple myeloma with a PD-1 or PD-L1 blocking antibody in combination with a thalidomide analogue plus dexamethasone is not recommended outside of controlled clinical trials. (5.4)
- Embryo-Fetal toxicity: Can cause fetal harm. Advise females of reproductive potential of the potential risk to a fetus and to use effective method of contraception. (5.5, 8.1, 8.3)

6 ADVERSE REACTIONS

The most common adverse reactions (≥20%) in patients treated with KEYTRUDA QLEX in combination with chemotherapy were nausea, fatigue, and musculoskeletal pain. (6.1)

The safety of KEYTRUDA QLEX for the approved indications is also based on the safety of intravenous pembrolizumab given as a single agent or in combination with other antitumor medicines.

The most common adverse reactions (reported in ≥20% of patients) with intravenous pembrolizumab were:

- As a single agent: fatigue, musculoskeletal pain, rash, diarrhea, pyrexia, cough, decreased appetite, pruritus, dyspnea, constipation, pain, abdominal pain, nausea, and hypothyroidism. (6.1)
- In combination with chemotherapy or chemoradiotherapy: fatigue/asthenia, nausea, constipation, diarrhea, decreased appetite, rash, vomiting, cough, dyspnea, pyrexia, alopecia, peripheral neuropathy, mucosal inflammation, stomatitis, headache, weight loss, abdominal pain, arthralgia, myalgia, insomnia, palmar-plantar erythrodysesthesia, urinary tract infection, hypothyroidism, radiation skin injury, dysphagia, dry mouth and musculoskeletal pain. (6.1)
- In combination with chemotherapy and bevacizumab: peripheral neuropathy, alopecia, anemia, fatigue/asthenia, nausea, neutropenia, diarrhea, hypertension, thrombocytopenia, constipation, arthralgia, vomiting, urinary tract infection, rash, leukopenia, hypothyroidism, decreased appetite, pyrexia, epistaxis, decreased white blood cell count, and stomatitis. (6.1)
- In combination with axitinib: diarrhea, fatigue/asthenia, hypertension, hepatotoxicity, hypothyroidism, decreased appetite, palmar-plantar erythrodysesthesia, nausea, stomatitis/mucosal inflammation, dysphonia, rash, cough, and constipation. (6.1)
- In combination with lenvatinib: hypothyroidism, hypertension, fatigue, diarrhea, musculoskeletal disorders, nausea, decreased appetite, vomiting, stomatitis, weight loss, abdominal pain, urinary tract infection, proteinuria, constipation, headache, hemorrhagic events, palmar-plantar erythrodysesthesia, dysphonia, rash, hepatotoxicity, and acute kidney injury. (6.1)
- In combination with enfortumab vedotin: rash, peripheral neuropathy, fatigue, pruritus, diarrhea, alopecia, weight loss, decreased appetite, dry eye, nausea, constipation, dysgeusia, and urinary tract infection. (6.1)

To report SUSPECTED ADVERSE REACTIONS, contact Merck Sharp & Dohme LLC at 1-877-888-4231 or FDA at 1-800-FDA-1088 or www.fda.gov/medwatch.

8 USE IN SPECIFIC POPULATIONS

Lactation: Advise not to breastfeed. (8.2)

FULL PRESCRIBING INFORMATION

1 INDICATIONS AND USAGE

1.1 Melanoma

KEYTRUDA QLEX™ is indicated for the treatment of adult patients with unresectable or metastatic melanoma.

KEYTRUDA QLEX is indicated for the adjuvant treatment of adult and pediatric patients 12 years and older with Stage IIB, IIC, or III melanoma following complete resection.

1.2 Non-Small Cell Lung Cancer

KEYTRUDA QLEX, in combination with pemetrexed and platinum chemotherapy, is indicated for the first-line treatment of adult patients with metastatic nonsquamous non-small cell lung cancer (NSCLC), with no EGFR or ALK genomic tumor aberrations.

KEYTRUDA QLEX, in combination with carboplatin and either paclitaxel or paclitaxel protein-bound, is indicated for the first-line treatment of adult patients with metastatic squamous NSCLC.

KEYTRUDA QLEX, as a single agent, is indicated for the first-line treatment of adult patients with NSCLC expressing PD-L1 [Tumor Proportion Score (TPS) ≥1%] as determined by an FDA-authorized test [see Dosage and Administration (2.1)], with no EGFR or ALK genomic tumor aberrations, and is:

- Stage III where patients are not candidates for surgical resection or definitive chemoradiation, or
- metastatic.

KEYTRUDA QLEX, as a single agent, is indicated for the treatment of adult patients with metastatic NSCLC whose tumors express PD-L1 (TPS ≥1%) as determined by an FDA-authorized test [see Dosage and Administration (2.1)], with disease progression on or after platinum-containing chemotherapy. Patients with EGFR or ALK genomic tumor aberrations should have disease progression on FDA-approved therapy for these aberrations prior to receiving KEYTRUDA QLEX.

KEYTRUDA QLEX is indicated for the treatment of adult patients with resectable (tumors ≥4 cm or node positive) NSCLC in combination with platinum-containing chemotherapy as neoadjuvant treatment, and then continued as a single agent as adjuvant treatment after surgery.

KEYTRUDA QLEX, as a single agent, is indicated as adjuvant treatment following resection and platinum-based chemotherapy for adult patients with Stage IB (T2a ≥4 cm), II, or IIIA NSCLC.

1.3 Malignant Pleural Mesothelioma

KEYTRUDA QLEX, in combination with pemetrexed and platinum chemotherapy, is indicated for the first-line treatment of adult patients with unresectable advanced or metastatic malignant pleural mesothelioma (MPM).

1.4 Head and Neck Squamous Cell Cancer

KEYTRUDA QLEX is indicated for the treatment of adult patients with resectable locally advanced HNSCC whose tumors express PD-L1 [Combined Positive Score (CPS) ≥1] as determined by an FDA-authorized test [see Dosage and Administration (2.1)], as a single agent as neoadjuvant treatment, continued as adjuvant treatment in combination with radiotherapy (RT) with or without cisplatin and then as a single agent.

KEYTRUDA QLEX, in combination with platinum and fluorouracil (FU), is indicated for the first-line treatment of adult patients with metastatic or with unresectable, recurrent head and neck squamous cell carcinoma (HNSCC).

KEYTRUDA QLEX, as a single agent, is indicated for the first-line treatment of adult patients with metastatic or with unresectable, recurrent HNSCC whose tumors express PD-L1 [Combined Positive Score (CPS) ≥1] as determined by an FDA-authorized test [see Dosage and Administration (2.1)].

KEYTRUDA QLEX, as a single agent, is indicated for the treatment of adult patients with recurrent or metastatic HNSCC with disease progression on or after platinum-containing chemotherapy.

1.5 Urothelial Cancer

KEYTRUDA QLEX, in combination with enfortumab vedotin, is indicated for the treatment of adult patients with locally advanced or metastatic urothelial cancer.

KEYTRUDA QLEX, as a single agent, is indicated for the treatment of adult patients with locally advanced or metastatic urothelial carcinoma:

- who are not eligible for any platinum-containing chemotherapy, or
- who have disease progression during or following platinum-containing chemotherapy or within 12 months of neoadjuvant or adjuvant treatment with platinum-containing chemotherapy.

KEYTRUDA QLEX, in combination with enfortumab vedotin, as neoadjuvant treatment and then continued after cystectomy as adjuvant treatment, is indicated for the treatment of adult patients with muscle invasive bladder cancer (MIBC) who are ineligible for cisplatin-containing chemotherapy.

KEYTRUDA QLEX, as a single agent, is indicated for the treatment of adult patients with Bacillus Calmette-Guerin (BCG)-unresponsive, high-risk, non-muscle invasive bladder cancer (NMIBC) with carcinoma in situ (CIS) with or without papillary tumors who are ineligible for or have elected not to undergo cystectomy.

1.6 Microsatellite Instability-High or Mismatch Repair Deficient Cancer

KEYTRUDA QLEX is indicated for the treatment of adult and pediatric patients 12 years and older with unresectable or metastatic microsatellite instability-high (MSI-H) or mismatch repair deficient (dMMR) solid tumors, as determined by an FDA-authorized test, that have progressed following prior treatment and who have no satisfactory alternative treatment options [see Dosage and Administration (2.1)].

1.7 Microsatellite Instability-High or Mismatch Repair Deficient Colorectal Cancer

KEYTRUDA QLEX is indicated for the treatment of adult patients with unresectable or metastatic MSI-H or dMMR colorectal cancer (CRC) as determined by an FDA-authorized test [see Dosage and Administration (2.1)].

1.8 Gastric Cancer

KEYTRUDA QLEX, in combination with trastuzumab, fluoropyrimidine- and platinum-containing chemotherapy, is indicated for the first-line treatment of adults with locally advanced unresectable or metastatic HER2-positive gastric or gastroesophageal junction (GEJ) adenocarcinoma whose tumors express PD-L1 (CPS ≥1) as determined by an FDA-authorized test [see Dosage and Administration (2.1)].

KEYTRUDA QLEX, in combination with fluoropyrimidine- and platinum-containing chemotherapy, is indicated for the first-line treatment of adults with locally advanced unresectable or metastatic HER2-negative gastric or gastroesophageal junction (GEJ) adenocarcinoma whose tumors express PD-L1 (CPS ≥ 1) as determined by an FDA-authorized test [see Dosage and Administration (2.1)].

1.9 Esophageal Cancer

KEYTRUDA QLEX is indicated for the treatment of adult patients with locally advanced or metastatic esophageal or gastroesophageal junction (GEJ) (tumors with epicenter 1 to 5 centimeters above the GEJ) carcinoma that is not amenable to surgical resection or definitive chemoradiation either:

- in combination with platinum- and fluoropyrimidine-based chemotherapy for patients with tumors that express PD-L1 (CPS ≥ 1) [see Dosage and Administration (2.1)], or
- as a single agent after one or more prior lines of systemic therapy for patients with tumors of squamous cell histology that express PD-L1 (CPS ≥10) as determined by an FDA-authorized test [see Dosage and Administration (2.1)].

1.10 Cervical Cancer

KEYTRUDA QLEX, in combination with chemoradiotherapy (CRT), is indicated for the treatment of adult patients with locally advanced cervical cancer involving the lower third of the vagina, with or without extension to pelvic sidewall, or hydronephrosis/non-functioning kidney, or spread to adjacent pelvic organs (FIGO 2014 Stage III-IVA).

KEYTRUDA QLEX, in combination with chemotherapy, with or without bevacizumab, is indicated for the treatment of adult patients with persistent, recurrent, or metastatic cervical cancer whose tumors express PD-L1 (CPS ≥1) as determined by an FDA-authorized test [see Dosage and Administration (2.1)].

KEYTRUDA QLEX, as a single agent, is indicated for the treatment of adult patients with recurrent or metastatic cervical cancer with disease progression on or after chemotherapy whose tumors express PD-L1 (CPS ≥1) as determined by an FDA-authorized test [see Dosage and Administration (2.1)].

1.11 Hepatocellular Carcinoma

KEYTRUDA QLEX is indicated for the treatment of adult patients with hepatocellular carcinoma (HCC) secondary to hepatitis B who have received prior systemic therapy other than a PD-1/PD-L1-containing regimen.

1.12 Biliary Tract Cancer

KEYTRUDA QLEX, in combination with gemcitabine and cisplatin, is indicated for the treatment of adult patients with locally advanced unresectable or metastatic biliary tract cancer (BTC).

1.13 Merkel Cell Carcinoma

KEYTRUDA QLEX is indicated for the treatment of adult and pediatric patients 12 years and older with recurrent locally advanced or metastatic Merkel cell carcinoma (MCC).

1.14 Renal Cell Carcinoma

KEYTRUDA QLEX, in combination with axitinib, is indicated for the first-line treatment of adult patients with advanced renal cell carcinoma (RCC).

KEYTRUDA QLEX, in combination with lenvatinib, is indicated for the first-line treatment of adult patients with advanced RCC.

KEYTRUDA QLEX is indicated for the adjuvant treatment of adult patients with RCC at intermediate-high or high risk of recurrence following nephrectomy, or following nephrectomy and resection of metastatic lesions [see Clinical Studies (14.15)].

1.15 Endometrial Carcinoma

KEYTRUDA QLEX, in combination with carboplatin and paclitaxel, followed by KEYTRUDA QLEX as a single agent, is indicated for the treatment of adult patients with primary advanced or recurrent endometrial carcinoma.

KEYTRUDA QLEX, in combination with lenvatinib, is indicated for the treatment of adult patients with advanced endometrial carcinoma that is mismatch repair proficient (pMMR) or not MSI-H as determined by an FDA-authorized test, who have disease progression following prior systemic therapy in any setting and are not candidates for curative surgery or radiation [see Dosage and Administration (2.1)].

KEYTRUDA QLEX, as a single agent, is indicated for the treatment of adult patients with advanced endometrial carcinoma that is MSI-H or dMMR, as determined by an FDA-authorized test, who have disease progression following prior systemic therapy in any setting and are not candidates for curative surgery or radiation [see Dosage and Administration (2.1)].

1.16 Tumor Mutational Burden-High Cancer

KEYTRUDA QLEX is indicated for the treatment of adult and pediatric patients 12 years and older with unresectable or metastatic tumor mutational burden-high (TMB-H) [≥10 mutations/megabase (mut/Mb)] solid tumors, as determined by an FDA-authorized test [see Dosage and Administration (2.1)], that have progressed following prior treatment and who have no satisfactory alternative treatment options.

This indication is approved under accelerated approval based on tumor response rate and durability of response [see Clinical Studies (14.17)]. Continued approval for this indication may be contingent upon verification and description of clinical benefit in the confirmatory trials.

Limitations of Use: The safety and effectiveness of KEYTRUDA QLEX in pediatric patients 12 years and older with TMB-H central nervous system cancers have not been established.

1.17 Cutaneous Squamous Cell Carcinoma

KEYTRUDA QLEX is indicated for the treatment of adult patients with recurrent or metastatic cutaneous squamous cell carcinoma (cSCC) or locally advanced cSCC that is not curable by surgery or radiation.

1.18 Triple-Negative Breast Cancer

KEYTRUDA QLEX is indicated for the treatment of adult patients with high-risk early-stage triple-negative breast cancer (TNBC) in combination with chemotherapy as neoadjuvant treatment, and then continued as a single agent as adjuvant treatment after surgery.

KEYTRUDA QLEX, in combination with chemotherapy, is indicated for the treatment of adult patients with locally recurrent unresectable or metastatic TNBC whose tumors express PD-L1 (CPS ≥10) as determined by an FDA-authorized test [see Dosage and Administration (2.1)].

1.19 Ovarian Cancer

KEYTRUDA QLEX, in combination with paclitaxel, with or without bevacizumab, is indicated for the treatment of adult patients with platinum-resistant epithelial ovarian, fallopian tube, or primary peritoneal carcinoma whose tumors express PD-L1 (CPS ≥1) as determined by an FDA-authorized test [see Dosage and Administration (2.1)], and who have received one or two prior systemic treatment regimens.

2 DOSAGE AND ADMINISTRATION

2.1 Patient Selection

See information on FDA-authorized tests for intravenous pembrolizumab. Information on FDA-authorized tests for patient selection is available at: http://www.fda.gov/CompanionDiagnostics.

Patient Selection for Single-Agent Treatment

Select patients for treatment with KEYTRUDA QLEX as a single agent based on the presence of positive PD-L1 expression in:

- Stage III NSCLC who are not candidates for surgical resection or definitive chemoradiation [see Clinical Studies (14.3)].
- metastatic NSCLC [see Clinical Studies (14.3)].
- first-line treatment of metastatic or unresectable, recurrent HNSCC [see Clinical Studies (14.5)].
- previously treated recurrent locally advanced or metastatic esophageal cancer [see Clinical Studies (14.10)].
- recurrent or metastatic cervical cancer with disease progression on or after chemotherapy [see Clinical Studies (14.11)].

For the MSI-H/dMMR indications, select patients for treatment with KEYTRUDA QLEX as a single agent based on MSI-H/dMMR status in tumor specimens [see Clinical Studies (14.7, 14.8)].

For the TMB-H indication, select patients for treatment with KEYTRUDA QLEX as a single agent based on TMB-H status in tumor specimens [see Clinical Studies (14.17)].

Because subclonal dMMR mutations and microsatellite instability may arise in high-grade gliomas during temozolomide therapy, it is recommended to test for TMB-H, MSI-H, and dMMR in the primary tumor specimens obtained prior to initiation of temozolomide chemotherapy in patients with high-grade gliomas.

Additional Patient Selection Information for MSI-H or dMMR in Patients with non-CRC Solid Tumors

Due to discordance between local tests and FDA-authorized tests, confirmation of MSI-H or dMMR status is recommended by an FDA-authorized test in patients with MSI-H or dMMR solid tumors, if feasible. If unable to perform confirmatory MSI-H/dMMR testing, the presence of TMB ≥10 mut/Mb, as determined by an FDA-authorized test, may be used to select patients for treatment [see Clinical Studies (14.7)].

Patient Selection for Combination Therapy

For use of KEYTRUDA QLEX as a single agent as neoadjuvant treatment, then in combination with radiotherapy (RT) with or without chemotherapy then continued as a single agent as adjuvant treatment, select patients based on presence of positive PD-L1 expression (CPS ≥1) in resectable locally advanced HNSCC [see Clinical Studies (14.5)].

For use of KEYTRUDA QLEX in combination with chemotherapy, select patients based on the presence of positive PD-L1 expression (CPS ≥1) in locally advanced unresectable or metastatic gastric or gastroesophageal junction (GEJ) adenocarcinoma, and esophageal or gastroesophageal junction (GEJ) carcinoma [see Clinical Studies (14.9), (14.10)].

- An FDA-authorized test for the detection of PD-L1 for the selection of patients with PD-L1 (CPS ≥1) expression in esophageal carcinoma in combination with platinum- and fluoropyrimidine-based chemotherapy is not available.

For use of KEYTRUDA QLEX in combination with chemotherapy, with or without bevacizumab, select patients based on the presence of positive PD-L1 expression in persistent, recurrent, or metastatic cervical cancer [see Clinical Studies (14.11)].

For the pMMR/not MSI-H advanced endometrial carcinoma indication, select patients for treatment with KEYTRUDA QLEX in combination with lenvatinib based on MMR or MSI status in tumor specimens [see Clinical Studies (14.16)].

For use of KEYTRUDA QLEX in combination with chemotherapy, select patients based on the presence of positive PD-L1 expression in locally recurrent unresectable or metastatic TNBC [see Clinical Studies (14.19)].

For use of KEYTRUDA QLEX in combination with paclitaxel, with or without bevacizumab, select patients based on the presence of positive PD-L1 expression (CPS ≥1) in platinum-resistant epithelial ovarian, fallopian tube, or primary peritoneal carcinoma [see Clinical Studies (14.20)].

2.2 Important Dosage and Administration Information

- KEYTRUDA QLEX has different recommended dosage and administration instructions than intravenous pembrolizumab.
  - To reduce the risk of medication errors, check the vial labels to ensure that the drug being prepared and administered is KEYTRUDA QLEX for subcutaneous use and not intravenous pembrolizumab.
  - Do not substitute KEYTRUDA QLEX with intravenous pembrolizumab because they have different recommended dosages and routes of administration.
  - Patients receiving intravenous pembrolizumab can switch to subcutaneous KEYTRUDA QLEX at their next scheduled dose.
  - Patients receiving subcutaneous KEYTRUDA QLEX can switch to intravenous pembrolizumab at their next scheduled dose.
  - Administer KEYTRUDA QLEX as a subcutaneous injection into the thigh or abdomen, avoiding the 5 cm area around the navel.
- Every 3-week dosing (395 mg/4,800 units): inject 2.4 mL subcutaneously over 1 minute. Treatment duration is provided in Recommended Dosage (Table 1).
- Every 6-week dosing (790 mg/9,600 units): inject 4.8 mL subcutaneously over 2 minutes. Treatment duration is provided in Recommended Dosage (Table 1).
- Inject into healthy skin and never into areas where the skin is red, bruised, tender, or hard.
- Ensure the injection site is at least 2.5 cm from the previous injection site.
- During treatment with KEYTRUDA QLEX, do not administer other medications for subcutaneous use at the same site as KEYTRUDA QLEX.
- Do not administer KEYTRUDA QLEX intravenously.
- KEYTRUDA QLEX must be administered by a healthcare provider.

2.3 Recommended Dosage

The recommended dosages of KEYTRUDA QLEX are presented in Table 1.

- Every 3-week dosing (395 mg pembrolizumab and 4,800 units berahyaluronidase alfa): inject 2.4 mL subcutaneously over 1 minute.
- Every 6-week dosing (790 mg pembrolizumab and 9,600 units berahyaluronidase alfa): inject 4.8 mL subcutaneously over 2 minutes.

Table 1: Recommended Dosage
Indication | Recommended Dosage of KEYTRUDA QLEX | Duration/Timing of Treatment
Monotherapy
Adult patients with unresectable or metastatic melanoma | 395 mg/4,800 units every 3 weeks or 790 mg/9,600 units every 6 weeks | Until disease progression or unacceptable toxicity
Adjuvant treatment of adult patients with melanoma, NSCLC, or RCC | 395 mg/4,800 units every 3 weeks or 790 mg/9,600 units every 6 weeks | Until disease recurrence, unacceptable toxicity, or up to 12 months
Adult patients with NSCLC, HNSCC, locally advanced or metastatic Urothelial Carcinoma, MSI-H or dMMR Cancer, MSI-H or dMMR CRC, MSI-H or dMMR Endometrial Carcinoma, Esophageal Cancer, Cervical Cancer, HCC, MCC, TMB-H Cancer, or cSCC | 395 mg/4,800 units every 3 weeks or 790 mg/9,600 units every 6 weeks | Until disease progression, unacceptable toxicity, or up to 24 months
Adult patients with high-risk BCG- unresponsive NMIBC | 395 mg/4,800 units every 3 weeks or 790 mg/9,600 units every 6 weeks | Until persistent or recurrent high-risk NMIBC, disease progression, unacceptable toxicity, or up to 24 months
Pediatric patients [The recommended dosage for melanoma, MSI-H or dMMR cancer, MCC and TMB-H cancer has not been established in pediatric patients 12 years and older who weigh 40 kg or less [see Use in Specific Populations (8.4)].] (12 years and older who weigh greater than 40 kg) with MSI-H or dMMR Cancer, MCC, or TMB- H Cancer | 395 mg/4,800 units every 3 weeks or 790 mg/9,600 units every 6 weeks | Until disease progression, unacceptable toxicity, or up to 24 months
Pediatric patients (12 years and older who weigh greater than 40 kg) for adjuvant treatment of melanoma | 395 mg/4,800 units every 3 weeks or 790 mg/9,600 units every 6 weeks | Until disease recurrence, unacceptable toxicity, or up to 12 months
Combination Therapy [Refer to the Prescribing Information for the agents administered in combination with KEYTRUDA QLEX for recommended dosing information, as appropriate.]
Adult patients with resectable NSCLC | 395 mg/4,800 units every 3 weeks or 790 mg/9,600 units every 6 weeks Administer KEYTRUDA QLEX prior to chemotherapy when given on the same day. | Neoadjuvant treatment in combination with chemotherapy for 12 weeks or until disease progression that precludes definitive surgery or unacceptable toxicity, followed by adjuvant treatment with KEYTRUDA QLEX as a single agent after surgery for 39 weeks or until disease recurrence or unacceptable toxicity
Adult patients with NSCLC, MPM, HNSCC, HER2-negative Gastric Cancer, Esophageal Cancer, or BTC | 395 mg/4,800 units every 3 weeks or 790 mg/9,600 units every 6 weeks Administer KEYTRUDA QLEX prior to chemotherapy when given on the same day. | Until disease progression, unacceptable toxicity, or up to 24 months
Adult patients with locally advanced or metastatic urothelial cancer | 395 mg/4,800 units every 3 weeks or 790 mg/9,600 units every 6 weeks Administer KEYTRUDA QLEX after enfortumab vedotin when given on the same day. | Until disease progression, unacceptable toxicity, or up to 24 months
Adult patients with locally advanced HNSCC | 395 mg/4,800 units every 3 weeks or 790 mg/9,600 units every 6 weeks Administer KEYTRUDA QLEX prior to cisplatin when given on the same day. | Neoadjuvant:; - Administer KEYTRUDA QLEX for 6 weeks or until disease progression that precludes definitive surgery or unacceptable toxicity.; Adjuvant:; - Administer KEYTRUDA QLEX in combination with RT with or without cisplatin. - Continue KEYTRUDA QLEX as a single agent.; Continue KEYTRUDA QLEX until disease recurrence or unacceptable toxicity or up to one year
Adult patients with MIBC | 395 mg/4,800 units every 3 weeks or 790 mg/9,600 units every 6 weeks Administer KEYTRUDA QLEX after enfortumab vedotin when given on the same day. | Neoadjuvant:; - Administer KEYTRUDA QLEX 395 mg/4,800 units every 3 weeks for 3 doses in combination with enfortumab vedotin or until disease progression that precludes curative-intent cystectomy or unacceptable toxicity.; Adjuvant:; - Administer KEYTRUDA QLEX 395 mg/4,800 units every 3 weeks for 14 doses or 790 mg/9,600 units every 6 weeks for 7 doses in combination with enfortumab vedotin or until disease recurrence or unacceptable toxicity
Adult patients with HER2-positive Gastric Cancer | 395 mg/4,800 units every 3 weeks or 790 mg/9,600 units every 6 weeks Administer KEYTRUDA QLEX prior to trastuzumab and chemotherapy when given on the same day. | Until disease progression, unacceptable toxicity, or up to 24 months
Adult patients with Cervical Cancer | 395 mg/4,800 units every 3 weeks or 790 mg/9,600 units every 6 weeks Administer KEYTRUDA QLEX prior to chemoradiotherapy or prior to chemotherapy with or without bevacizumab when given on the same day. | Until disease progression, unacceptable toxicity, or for KEYTRUDA QLEX, up to 24 months
Adult patients with RCC | 395 mg/4,800 units every 3 weeks or 790 mg/9,600 units every 6 weeks Administer KEYTRUDA QLEX in combination with axitinib 5 mg orally twice daily [When axitinib is used in combination with KEYTRUDA QLEX, dose escalation of axitinib above the initial 5 mg dose may be considered at intervals of six weeks or longer.] or Administer KEYTRUDA QLEX in combination with lenvatinib 20 mg orally once daily. | Until disease progression, unacceptable toxicity, or for KEYTRUDA QLEX, up to 24 months
Adult patients with Endometrial Carcinoma | 395 mg/4,800 units every 3 weeks or 790 mg/9,600 units every 6 weeks Administer KEYTRUDA QLEX prior to carboplatin and paclitaxel when given on the same day. or Administer KEYTRUDA QLEX in combination with lenvatinib 20 mg orally once daily. | Until disease progression, unacceptable toxicity, or for KEYTRUDA QLEX, up to 24 months
Adult patients with high-risk early-stage TNBC | 395 mg/4,800 units every 3 weeks or 790 mg/9,600 units every 6 weeks Administer KEYTRUDA QLEX prior to chemotherapy when given on the same day. | Neoadjuvant treatment in combination with chemotherapy for 24 weeks (8 doses of 395 mg/4,800 units every 3 weeks or 4 doses of 790 mg/9,600 units every 6 weeks) or until disease progression or unacceptable toxicity, followed by adjuvant treatment with KEYTRUDA QLEX as a single agent for up to 27 weeks (9 doses of 395 mg/4,800 units every 3 weeks or 5 doses of 790 mg/9,600 units every 6 weeks) or until disease recurrence or unacceptable toxicity [Patients who experience disease progression or unacceptable toxicity related to KEYTRUDA QLEX with neoadjuvant treatment in combination with chemotherapy should not receive adjuvant single agent KEYTRUDA QLEX.]
Adult patients with locally recurrent unresectable or metastatic TNBC | 395 mg/4,800 units every 3 weeks or 790 mg/9,600 units every 6 weeks Administer KEYTRUDA QLEX prior to chemotherapy when given on the same day. | Until disease progression, unacceptable toxicity, or up to 24 months
Adult patients with Ovarian Cancer | 395 mg/4,800 units every 3 weeks or 790 mg/9,600 units every 6 weeks Administer KEYTRUDA QLEX prior to paclitaxel with or without bevacizumab when given on the same day. | Until disease progression, unacceptable toxicity, or up to 24 months

2.4 Dosage Modifications

No dose reduction for KEYTRUDA QLEX is recommended. In general, withhold KEYTRUDA QLEX for severe (Grade 3) immune-mediated adverse reactions. Permanently discontinue KEYTRUDA QLEX for Life-threatening (Grade 4) immune-mediated adverse reactions, recurrent severe (Grade 3) immune-mediated reactions that require systemic immunosuppressive treatment, or an inability to reduce corticosteroid dose to 10 mg or less of prednisone or equivalent per day within 12 weeks of initiating steroids.

Dosage modifications for KEYTRUDA QLEX for adverse reactions that require management different from these general guidelines are summarized in Table 2.

Table 2: Recommended Dosage Modifications for Adverse Reactions
Adverse Reaction | Severity [Based on Common Terminology Criteria for Adverse Events (CTCAE), version 4.0] | Dosage Modification
Immune-Mediated Adverse Reactions [see Warnings and Precautions (5.1)]
Pneumonitis | Grade 2 | Withhold [Resume in patients with complete or partial resolution (Grades 0 to 1) after corticosteroid taper. Permanently discontinue if no complete or partial resolution within 12 weeks of initiating steroids or inability to reduce prednisone to 10 mg per day or less (or equivalent) within 12 weeks of initiating steroids.]
Pneumonitis | Grade 3 or 4 | Permanently discontinue
Colitis | Grade 2 or 3 | Withhold
Colitis | Grade 4 | Permanently discontinue
Hepatitis with no tumor involvement of the liver | AST or ALT increases to more than 3 and up to 8 times ULN or Total bilirubin increases to more than 1.5 and up to 3 times ULN | Withhold
For liver enzyme elevations in patients treated with combination therapy with axitinib, see Table 3. | AST or ALT increases to more than 8 times ULN or Total bilirubin increases to more than 3 times ULN | Permanently discontinue
Hepatitis with tumor involvement of the liver [If AST and ALT are less than or equal to ULN at baseline, withhold or permanently discontinue KEYTRUDA QLEX based on recommendations for hepatitis with no liver involvement.] | Baseline AST or ALT is more than 1 and up to 3 times ULN and increases to more than 5 and up to 10 times ULN or Baseline AST or ALT is more than 3 and up to 5 times ULN and increases to more than 8 and up to 10 times ULN | Withhold
Hepatitis with tumor involvement of the liver [If AST and ALT are less than or equal to ULN at baseline, withhold or permanently discontinue KEYTRUDA QLEX based on recommendations for hepatitis with no liver involvement.] | ALT or AST increases to more than 10 times ULN or Total bilirubin increases to more than 3 times ULN | Permanently discontinue
Endocrinopathies | Grade 3 or 4 | Withhold until clinically stable or permanently discontinue depending on severity
Nephritis with Renal Dysfunction | Grade 2 or 3 increased blood creatinine | Withhold
Nephritis with Renal Dysfunction | Grade 4 increased blood creatinine | Permanently discontinue
Exfoliative Dermatologic Conditions | Suspected SJS, TEN, or DRESS | Withhold
Exfoliative Dermatologic Conditions | Confirmed SJS, TEN, or DRESS | Permanently discontinue
Myocarditis | Grade 2, 3, or 4 | Permanently discontinue
Neurological Toxicities | Grade 2 | Withhold
Neurological Toxicities | Grade 3 or 4 | Permanently discontinue
Other Adverse Reactions
Hypersensitivity and Administration-Related Systemic Reactions [see Warnings and Precautions (5.2)] | Grade 1 or 2 | Interrupt injection (if not already fully administered). If symptoms resolve, resume injection
Hypersensitivity and Administration-Related Systemic Reactions [see Warnings and Precautions (5.2)] | Grade 3 or 4 | Permanently discontinue
ALT = alanine aminotransferase, AST = aspartate aminotransferase, DRESS = Drug Rash with Eosinophilia and Systemic Symptoms, SJS = Stevens Johnson Syndrome, TEN = toxic epidermal necrolysis, ULN = upper limit normal

The following table represents dosage modifications that are different from those described above for KEYTRUDA QLEX or in the Full Prescribing Information for the drug administered in combination.

Table 3: Recommended Specific Dosage Modifications for Adverse Reactions for KEYTRUDA QLEX in Combination with Axitinib
Treatment | Adverse Reaction | Severity | Dosage Modification
KEYTRUDA QLEX in combination with axitinib | Liver enzyme elevations [Consider corticosteroid therapy] | ALT or AST increases to at least 3 times but less than 10 times ULN without concurrent total bilirubin at least 2 times ULN | Withhold both KEYTRUDA QLEX and axitinib until resolution to Grades 0 or 1 [Based on Common Terminology Criteria for Adverse Events (CTCAE), version 4.0. Consider rechallenge with a single drug or sequential rechallenge with both drugs after recovery. If rechallenging with axitinib, consider dose reduction as per the axitinib Prescribing Information.]
KEYTRUDA QLEX in combination with axitinib | Liver enzyme elevations [Consider corticosteroid therapy] | ALT or AST increases to more than 3 times ULN with concurrent total bilirubin at least 2 times ULN or ALT or AST ≥10 times ULN | Permanently discontinue both KEYTRUDA QLEX and axitinib
ALT = alanine aminotransferase, AST = aspartate aminotransferase, ULN = upper limit normal

Recommended Dose Modifications for Adverse Reactions for KEYTRUDA QLEX in Combination with Lenvatinib

When administering KEYTRUDA QLEX in combination with lenvatinib, modify the dosage of one or both drugs. Withhold or discontinue KEYTRUDA QLEX as shown in Table 2. Refer to lenvatinib prescribing information for additional dose modification information.

2.5 Preparation

KEYTRUDA QLEX is a ready-to-use solution. Do not dilute KEYTRUDA QLEX.

Do not shake.

Preparation of the Syringe

- Remove KEYTRUDA QLEX vial from refrigerated storage [2°C to 8°C (36°F to 46°F)] and allow it to equilibrate to room temperature [20°C to 25°C (68°F to 77°F)] for at least 30 minutes.
- Prior to preparation for administration, if needed, the unpunctured vial may be stored at room temperature for up to 24 hours.
- Parenteral drug products should be inspected visually for particulate matter and discoloration prior to administration, whenever solution and container permit. The solution is clear to slightly opalescent, colorless to slightly yellow. Discard the vial if visible particles are observed.
- Use a sterile, polypropylene or polycarbonate syringe and a stainless steel transfer needle (18 to 21 gauge) to withdraw KEYTRUDA QLEX from the vial.
  - Every 3-week dosing (395 mg pembrolizumab/4,800 units berahyaluronidase alfa): withdraw 2.4 mL into the syringe.
  - Every 6-week dosing (790 mg pembrolizumab/9,600 units berahyaluronidase alfa): withdraw 4.8 mL into the syringe.
- To avoid needle clogging, change the needle to a 25 to 30 gauge, ½-inch, stainless steel hypodermic injection needle immediately prior to subcutaneous injection.
- Discard any unused portion left in the vial.

Storage of Prepared Syringe

The product does not contain a preservative and should be used immediately after withdrawing from the vial. If not used immediately, store the syringe containing KEYTRUDA QLEX with the transfer needle and cap in place:

- At room temperature 20°C to 25°C (68°F to 77°F) for up to 8 hours, or
- In the refrigerator at 2°C to 8°C (36°F to 46°F) for up to 24 hours. The 24-hour period may include up to 8 hours at room temperature.

Discard if storage time exceeds these limits.

If refrigerated, allow the filled syringe to come to room temperature for at least 30 minutes prior to administration.

Do not freeze.

3 DOSAGE FORMS AND STRENGTHS

KEYTRUDA QLEX is a clear to slightly opalescent, colorless to slightly yellow solution provided as:

- Injection: 395 mg pembrolizumab and 4,800 units berahyaluronidase alfa per 2.4 mL (165 mg/2,000 units per mL) in a single-dose vial
- Injection: 790 mg pembrolizumab and 9,600 units berahyaluronidase alfa per 4.8 mL (165 mg/2,000 units per mL) in a single-dose vial

4 CONTRAINDICATIONS

KEYTRUDA QLEX is contraindicated in patients with known hypersensitivity to berahyaluronidase alfa, hyaluronidase or to any of its excipients.

5 WARNINGS AND PRECAUTIONS

5.1 Severe and Fatal Immune-Mediated Adverse Reactions

KEYTRUDA QLEX is a monoclonal antibody that belongs to a class of drugs that bind to either the programmed death-receptor 1 (PD-1) or the PD-ligand 1 (PD-L1), blocking the PD-1/PD-L1 pathway, thereby removing inhibition of the immune response, potentially breaking peripheral tolerance and inducing immune-mediated adverse reactions. Important immune-mediated adverse reactions listed under WARNINGS AND PRECAUTIONS may not include all possible severe and fatal immune-mediated adverse reactions.

Immune-mediated adverse reactions, which may be severe or fatal, can occur in any organ system or tissue and can affect more than one body system simultaneously. Immune-mediated adverse reactions can occur at any time after starting treatment with a PD-1/PD-L1 blocking antibody. While immune-mediated adverse reactions usually manifest during treatment with PD-1/PD-L1 blocking antibodies, immune-mediated adverse reactions can also manifest after discontinuation of PD-1/PD-L1 blocking antibodies.

Early identification and management of immune-mediated adverse reactions are essential to ensure safe use of PD-1/PD-L1 blocking antibodies. Monitor patients closely for symptoms and signs that may be clinical manifestations of underlying immune-mediated adverse reactions. Evaluate liver enzymes, creatinine, and thyroid function at baseline and periodically during treatment. For patients with TNBC treated with KEYTRUDA QLEX in the neoadjuvant setting, monitor blood cortisol at baseline, prior to surgery, and as clinically indicated. In cases of suspected immune-mediated adverse reactions, initiate appropriate workup to exclude alternative etiologies, including infection. Institute medical management promptly, including specialty consultation as appropriate.

Withhold or permanently discontinue KEYTRUDA QLEX depending on severity [see Dosage and Administration (2.4)]. In general, if KEYTRUDA QLEX requires interruption or discontinuation, administer systemic corticosteroid therapy (1 to 2 mg/kg/day prednisone or equivalent) until improvement to Grade 1 or less. Upon improvement to Grade 1 or less, initiate corticosteroid taper and continue to taper over at least 1 month. Consider administration of other systemic immunosuppressants in patients whose immune-mediated adverse reactions are not controlled with corticosteroid therapy.

Toxicity management guidelines for adverse reactions that do not necessarily require systemic steroids (e.g., endocrinopathies and dermatologic reactions) are discussed below.

Immune-Mediated Pneumonitis

KEYTRUDA QLEX can cause immune-mediated pneumonitis. The incidence of pneumonitis is higher in patients who have received prior thoracic radiation. Immune-mediated pneumonitis occurred in 5% (13/251) of patients receiving KEYTRUDA QLEX in combination with chemotherapy, including fatal (0.4%), Grade 3 (2%), and Grade 2 (1.2%) adverse reactions.

Intravenous Pembrolizumab as a Single Agent

Immune-mediated pneumonitis occurred in 3.4% (94/2799) of patients receiving intravenous pembrolizumab, including fatal (0.1%), Grade 4 (0.3%), Grade 3 (0.9%), and Grade 2 (1.3%) adverse reactions. Systemic corticosteroids were required in 67% (63/94) of patients with pneumonitis. Pneumonitis led to permanent discontinuation of intravenous pembrolizumab in 1.3% (36) of patients and withholding of intravenous pembrolizumab in 0.9% (26) of patients. All patients who were withheld reinitiated intravenous pembrolizumab after symptom improvement; of these, 23% had recurrence of pneumonitis. Pneumonitis resolved in 59% of the 94 patients.

In a clinical study enrolling 580 adult patients with resected NSCLC (KEYNOTE-091) who received intravenous pembrolizumab as a single agent for adjuvant treatment, pneumonitis occurred in 41 (7%) patients, including fatal (0.2%), Grade 4 (0.3%), and Grade 3 (1%) adverse reactions. Patients received high-dose corticosteroids for a median duration of 10 days (range: 1 day to 2.3 months). Pneumonitis led to discontinuation of intravenous pembrolizumab in 26 (4.5%) of patients. Of the patients who developed pneumonitis, 54% interrupted intravenous pembrolizumab, 63% discontinued intravenous pembrolizumab, and 71% had resolution.

Immune-Mediated Colitis

KEYTRUDA QLEX can cause immune-mediated colitis, which may present with diarrhea. Cytomegalovirus (CMV) infection/reactivation has been reported in patients with corticosteroid-refractory immune-mediated colitis. In cases of corticosteroid-refractory colitis, consider repeating infectious workup to exclude alternative etiologies. Immune-mediated colitis occurred in 1.2% (3/251) of patients receiving KEYTRUDA QLEX in combination with chemotherapy, including Grade 3 (0.8%), and Grade 2 (0.4%) adverse reactions.

Intravenous Pembrolizumab as a Single Agent

Immune-mediated colitis occurred in 1.7% (48/2799) of patients receiving intravenous pembrolizumab, including Grade 4 (<0.1%), Grade 3 (1.1%), and Grade 2 (0.4%) adverse reactions. Systemic corticosteroids were required in 69% (33/48) of patients with colitis. Additional immunosuppressant therapy was required in 4.2% of patients. Colitis led to permanent discontinuation of intravenous pembrolizumab in 0.5% (15) of patients and withholding of intravenous pembrolizumab in 0.5% (13) of patients. All patients who were withheld reinitiated intravenous pembrolizumab after symptom improvement; of these, 23% had recurrence of colitis. Colitis resolved in 85% of the 48 patients.

Hepatotoxicity and Immune-Mediated Hepatitis

KEYTRUDA QLEX can cause immune-mediated hepatitis. Immune-mediated hepatitis occurred in 0.4% (1/251) of patients receiving KEYTRUDA QLEX in combination with chemotherapy, including Grade 2 (0.4%) adverse reactions.

Intravenous Pembrolizumab as a Single Agent

Immune-mediated hepatitis occurred in 0.7% (19/2799) of patients receiving intravenous pembrolizumab, including Grade 4 (<0.1%), Grade 3 (0.4%), and Grade 2 (0.1%) adverse reactions. Systemic corticosteroids were required in 68% (13/19) of patients with hepatitis. Eleven percent of these patients required additional immunosuppressant therapy. Hepatitis led to permanent discontinuation of intravenous pembrolizumab in 0.2% (6) of patients and withholding of intravenous pembrolizumab in 0.3% (9) of patients. All patients who were withheld reinitiated intravenous pembrolizumab after symptom improvement; of these, none had recurrence of hepatitis. Hepatitis resolved in 79% of the 19 patients.

In Combination with Axitinib

KEYTRUDA QLEX in combination with axitinib can cause hepatic toxicity with higher than expected frequencies of Grades 3 and 4 ALT and AST elevations compared to KEYTRUDA QLEX alone. Monitor liver enzymes before initiation of and periodically throughout treatment. Consider more frequent monitoring of liver enzymes as compared to when the drugs are administered as single agents. For elevated liver enzymes, interrupt KEYTRUDA QLEX and axitinib, and consider administering corticosteroids as needed [see Dosage and Administration (2.4)].

Intravenous Pembrolizumab in Combination with Axitinib

With the combination of intravenous pembrolizumab and axitinib, Grades 3 and 4 increased ALT (20%) and increased AST (13%) were seen. Fifty-nine percent of the patients with increased ALT received systemic corticosteroids. In patients with ALT ≥3 times ULN (Grades 2-4, n=116), ALT resolved to Grades 0-1 in 94%. Among the 92 patients who were rechallenged with either intravenous pembrolizumab (n=3) or axitinib (n=34) administered as a single agent or with both (n=55), recurrence of ALT ≥3 times ULN was observed in 1 patient receiving intravenous pembrolizumab, 16 patients receiving axitinib, and 24 patients receiving both intravenous pembrolizumab and axitinib. All patients with a recurrence of ALT ≥3 ULN subsequently recovered from the event.

Immune-Mediated Endocrinopathies

Adrenal Insufficiency

KEYTRUDA QLEX can cause primary or secondary adrenal insufficiency. For Grade 2 or higher adrenal insufficiency, initiate symptomatic treatment, including hormone replacement as clinically indicated. Withhold KEYTRUDA QLEX depending on severity [see Dosage and Administration (2.4)].

Adrenal insufficiency occurred in 2% (5/251) of patients receiving KEYTRUDA QLEX in combination with chemotherapy, including Grade 3 (0.4%), and Grade 2 (0.8%) adverse reactions.

Intravenous Pembrolizumab as a Single Agent

Adrenal insufficiency occurred in 0.8% (22/2799) of patients receiving intravenous pembrolizumab, including Grade 4 (<0.1%), Grade 3 (0.3%), and Grade 2 (0.3%) adverse reactions. Systemic corticosteroids were required in 77% (17/22) of patients with adrenal insufficiency; of these, the majority remained on systemic corticosteroids. Adrenal insufficiency led to permanent discontinuation of intravenous pembrolizumab in <0.1% (1) of patients and withholding of intravenous pembrolizumab in 0.3% (8) of patients. All patients who were withheld reinitiated intravenous pembrolizumab after symptom improvement.

Hypophysitis

KEYTRUDA QLEX can cause immune-mediated hypophysitis. Hypophysitis can present with acute symptoms associated with mass effect such as headache, photophobia, or visual field defects. Hypophysitis can cause hypopituitarism. Initiate hormone replacement as indicated. Withhold or permanently discontinue KEYTRUDA QLEX depending on severity [see Dosage and Administration (2.4)].

Intravenous Pembrolizumab as a Single Agent

Hypophysitis occurred in 0.6% (17/2799) of patients receiving intravenous pembrolizumab, including Grade 4 (<0.1%), Grade 3 (0.3%), and Grade 2 (0.2%) adverse reactions. Systemic corticosteroids were required in 94% (16/17) of patients with hypophysitis; of these, the majority remained on systemic corticosteroids. Hypophysitis led to permanent discontinuation of intravenous pembrolizumab in 0.1% (4) of patients and withholding of intravenous pembrolizumab in 0.3% (7) of patients. All patients who were withheld reinitiated intravenous pembrolizumab after symptom improvement.

Thyroid Disorders

KEYTRUDA QLEX can cause immune-mediated thyroid disorders. Thyroiditis can present with or without endocrinopathy. Hypothyroidism can follow hyperthyroidism. Initiate hormone replacement for hypothyroidism or institute medical management of hyperthyroidism as clinically indicated. Withhold or permanently discontinue KEYTRUDA QLEX depending on severity [see Dosage and Administration (2.4)].

Thyroiditis occurred in 0.4% (1/251) of patients receiving KEYTRUDA QLEX in combination with chemotherapy, including Grade 2 (0.4%). Hyperthyroidism occurred in 8% (20/251) of patients receiving KEYTRUDA QLEX in combination with chemotherapy, including Grade 2 (3.2%). Hypothyroidism occurred in 14% (35/251) of patients receiving KEYTRUDA QLEX in combination with chemotherapy, including Grade 2 (11%).

Intravenous Pembrolizumab as a Single Agent

Thyroiditis occurred in 0.6% (16/2799) of patients receiving intravenous pembrolizumab, including Grade 2 (0.3%). No patients discontinued intravenous pembrolizumab due to thyroiditis. Intravenous pembrolizumab was withheld in <0.1% (1) of patients.

Hyperthyroidism occurred in 3.4% (96/2799) of patients receiving intravenous pembrolizumab, including Grade 3 (0.1%) and Grade 2 (0.8%). Hyperthyroidism led to permanent discontinuation of intravenous pembrolizumab in <0.1% (2) of patients and withholding of intravenous pembrolizumab in 0.3% (7) of patients. All patients who were withheld reinitiated intravenous pembrolizumab after symptom improvement.

The incidence of new or worsening hyperthyroidism was higher in 580 patients with resected NSCLC, occurring in 11% of patients receiving intravenous pembrolizumab as a single agent as adjuvant treatment (KEYNOTE-091), including Grade 3 (0.2%) hyperthyroidism.

Hypothyroidism occurred in 8% (237/2799) of patients receiving intravenous pembrolizumab, including Grade 3 (0.1%) and Grade 2 (6.2%). Hypothyroidism led to permanent discontinuation of intravenous pembrolizumab in <0.1% (1) of patients and withholding of intravenous pembrolizumab in 0.5% (14) of patients. All patients who were withheld reinitiated intravenous pembrolizumab after symptom improvement. The majority of patients with hypothyroidism required long-term thyroid hormone replacement.

The incidence of new or worsening hypothyroidism was higher in 1185 patients with HNSCC, occurring in 16% of patients receiving intravenous pembrolizumab as a single agent or in combination with platinum and FU, including Grade 3 (0.3%) hypothyroidism.

The incidence of new or worsening hypothyroidism was higher in 580 patients with resected NSCLC, occurring in 22% of patients receiving intravenous pembrolizumab as a single agent as adjuvant treatment (KEYNOTE-091), including Grade 3 (0.3%) hypothyroidism.

Type 1 Diabetes Mellitus, which can present with Diabetic Ketoacidosis

Monitor patients for hyperglycemia or other signs and symptoms of diabetes. Initiate treatment with insulin as clinically indicated. Withhold KEYTRUDA QLEX depending on severity [see Dosage and Administration (2.4)].

Type 1 diabetes mellitus occurred in 0.4% (1/251) of patients receiving KEYTRUDA QLEX in combination with chemotherapy.

Intravenous Pembrolizumab as a Single Agent

Type 1 diabetes mellitus occurred in 0.2% (6/2799) of patients receiving intravenous pembrolizumab. Type 1 diabetes mellitus led to permanent discontinuation in <0.1% (1) of patients and withholding of intravenous pembrolizumab in <0.1% (1) of patients. All patients who were withheld reinitiated intravenous pembrolizumab after symptom improvement. All patients with Type 1 diabetes mellitus required long-term insulin therapy.

Immune-Mediated Nephritis with Renal Dysfunction

KEYTRUDA QLEX can cause immune-mediated nephritis.

Intravenous Pembrolizumab as a Single Agent

Immune-mediated nephritis occurred in 0.3% (9/2799) of patients receiving intravenous pembrolizumab, including Grade 4 (<0.1%), Grade 3 (0.1%), and Grade 2 (0.1%) adverse reactions. Systemic corticosteroids were required in 89% (8/9) of patients with nephritis. Nephritis led to permanent discontinuation of intravenous pembrolizumab in 0.1% (3) of patients and withholding of intravenous pembrolizumab in 0.1% (3) of patients. All patients who were withheld reinitiated intravenous pembrolizumab after symptom improvement; of these, none had recurrence of nephritis. Nephritis resolved in 56% of the 9 patients.

Immune-Mediated Dermatologic Adverse Reactions

KEYTRUDA QLEX can cause immune-mediated rash or dermatitis. Exfoliative dermatitis, including Stevens Johnson Syndrome, DRESS, and toxic epidermal necrolysis (TEN), has occurred with PD-1/PD-L1 blocking antibodies. Topical emollients and/or topical corticosteroids may be adequate to treat mild to moderate non-exfoliative rashes. Withhold or permanently discontinue KEYTRUDA QLEX depending on severity [see Dosage and Administration (2.4)].

Immune-mediated dermatologic adverse reactions occurred in 1.6% (4/251) of patients receiving KEYTRUDA QLEX in combination with chemotherapy, including Grade 4 (0.8%), and Grade 3 (0.8%) adverse reactions.

Intravenous Pembrolizumab as a Single Agent

Immune-mediated dermatologic adverse reactions occurred in 1.4% (38/2799) of patients receiving intravenous pembrolizumab, including Grade 3 (1%) and Grade 2 (0.1%) adverse reactions. Systemic corticosteroids were required in 40% (15/38) of patients with immune-mediated dermatologic adverse reactions. Immune-mediated dermatologic adverse reactions led to permanent discontinuation of intravenous pembrolizumab in 0.1% (2) of patients and withholding of intravenous pembrolizumab in 0.6% (16) of patients. All patients who were withheld reinitiated intravenous pembrolizumab after symptom improvement; of these, 6% had recurrence of immune-mediated dermatologic adverse reactions. Immune-mediated dermatologic adverse reactions resolved in 79% of the 38 patients.

Other Immune-Mediated Adverse Reactions

The following clinically significant immune-mediated adverse reactions occurred at an incidence of <1% (unless otherwise noted) in patients who received KEYTRUDA QLEX, intravenous pembrolizumab, or were reported with the use of other PD-1/PD-L1 blocking antibodies. Severe or fatal cases have been reported for some of these adverse reactions.

Cardiac/Vascular: Myocarditis, pericarditis, vasculitis

Nervous System: Meningitis, encephalitis, myelitis and demyelination, myasthenic syndrome/myasthenia gravis (including exacerbation), Guillain-Barré syndrome, nerve paresis, autoimmune neuropathy

Ocular: Uveitis, iritis and other ocular inflammatory toxicities can occur. Some cases can be associated with retinal detachment. Various grades of visual impairment, including blindness, can occur. If uveitis occurs in combination with other immune-mediated adverse reactions, consider a Vogt-Koyanagi-Harada-like syndrome, as this may require treatment with systemic steroids to reduce the risk of permanent vision loss.

Gastrointestinal: Pancreatitis, to include increases in serum amylase and lipase levels, gastritis (2.8%), duodenitis

Musculoskeletal and Connective Tissue: Myositis/polymyositis, rhabdomyolysis (and associated sequelae, including renal failure), arthritis (1.5%), polymyalgia rheumatica

Endocrine: Hypoparathyroidism

Hematologic/Immune: Hemolytic anemia, aplastic anemia, hemophagocytic lymphohistiocytosis, systemic inflammatory response syndrome, histiocytic necrotizing lymphadenitis (Kikuchi lymphadenitis), sarcoidosis, immune thrombocytopenic purpura, solid organ transplant rejection, other transplant (including corneal graft) rejection

5.2 Hypersensitivity and Administration-Related Reactions

KEYTRUDA QLEX can cause severe or life-threatening administration-related reactions, including hypersensitivity and anaphylaxis. In Study MK-3475A-D77, hypersensitivity and administration-related systemic reactions occurred in 3.2% (8/251) of patients receiving KEYTRUDA QLEX, including Grade 2 (2.8%). Monitor patients for signs and symptoms of administration-related systemic reactions including rigors, chills, wheezing, pruritus, flushing, rash, hypotension, hypoxemia, and fever. Interrupt injection (if not already fully administered) and resume if symptoms resolve for mild or moderate hypersensitivity and administration-related systemic reactions. For severe or life-threatening hypersensitivity and administration-related systemic reactions, stop injection and permanently discontinue KEYTRUDA QLEX [see Dosage and Administration (2.4)].

5.3 Complications of Allogeneic HSCT

Fatal and other serious complications can occur in patients who receive allogeneic hematopoietic stem cell transplantation (HSCT) before or after being treated with a PD-1/PD-L1 blocking antibody. Transplant-related complications include hyperacute graft-versus-host-disease (GVHD), acute GVHD, chronic GVHD, hepatic veno-occlusive disease (VOD) after reduced intensity conditioning, and steroid-requiring febrile syndrome (without an identified infectious cause). These complications may occur despite intervening therapy between PD-1/PD-L1 blockade and allogeneic HSCT.

Follow patients closely for evidence of transplant-related complications and intervene promptly. Consider the benefit versus risks of treatment with a PD-1/PD-L1 blocking antibody prior to or after an allogeneic HSCT.

5.4 Increased Mortality in Patients with Multiple Myeloma when Pembrolizumab is Added to a Thalidomide Analogue and Dexamethasone

In two randomized trials in patients with multiple myeloma, the addition of intravenous pembrolizumab to a thalidomide analogue plus dexamethasone, a use for which no PD-1 or PD-L1 blocking antibody is indicated, resulted in increased mortality. Treatment of patients with multiple myeloma with a PD-1 or PD-L1 blocking antibody in combination with a thalidomide analogue plus dexamethasone is not recommended outside of controlled trials.

5.5 Embryo-Fetal Toxicity

Based on its mechanism of action, KEYTRUDA QLEX can cause fetal harm when administered to a pregnant woman. Animal studies have demonstrated that inhibition of the PD-L1/PD-1 pathway can lead to increased risk of immune-related rejection of the developing fetus resulting in fetal death. Advise pregnant women and females of reproductive potential of the potential risk to a fetus. Advise females of reproductive potential to use effective contraception during treatment with KEYTRUDA QLEX and for 4 months after the last dose [see Use in Specific Populations (8.1, 8.3)].

6 ADVERSE REACTIONS

The following clinically significant adverse reactions are described elsewhere in the labeling.

- Severe and fatal immune-mediated adverse reactions [see Warnings and Precautions (5.1)].
- Hypersensitivity and Administration-Related Reactions [see Warnings and Precautions (5.2)].

6.1 Clinical Trials Experience

Because clinical trials are conducted under widely varying conditions, adverse reaction rates observed in the clinical trials of a drug cannot be directly compared to rates in the clinical trials of another drug and may not reflect the rates observed in practice.

The data described in the WARNINGS AND PRECAUTIONS reflect exposure to intravenous pembrolizumab as a single agent in 2799 patients in three randomized, open-label, active-controlled trials (KEYNOTE-002, KEYNOTE-006, and KEYNOTE-010), which enrolled 912 patients with melanoma and 682 patients with NSCLC, and one single-arm trial (KEYNOTE-001), which enrolled 655 patients with melanoma and 550 patients with NSCLC. In addition to the 2799 patients, certain subsections in the WARNINGS AND PRECAUTIONS describe adverse reactions observed with exposure to KEYTRUDA QLEX in combination with platinum doublet chemotherapy in a randomized, open-label, active-controlled trial (Study MK-3475A-D77), which enrolled 251 patients with NSCLC; intravenous pembrolizumab as a single agent in a randomized, placebo-controlled trial (KEYNOTE-091), which enrolled 580 patients with resected NSCLC; a non-randomized, open-label, multi-cohort trial (KEYNOTE-012), a non-randomized, open-label, single-cohort trial (KEYNOTE-055), and two randomized, open-label, active-controlled trials (KEYNOTE-040 and KEYNOTE-048 single agent arms), which enrolled 909 patients with HNSCC; in a randomized, open-label, active-controlled trial (KEYNOTE-048 combination arm), which enrolled 276 patients with HNSCC; in combination with axitinib in a randomized, active-controlled trial (KEYNOTE-426), which enrolled 429 patients with RCC; and in post-marketing use. Across all trials, patients were administered either KEYTRUDA QLEX 790 mg/9,600 units every 6 weeks or intravenous pembrolizumab at doses of 2 mg/kg every 3 weeks, 10 mg/kg every 2 weeks, 10 mg/kg every 3 weeks, or 200 mg every 3 weeks. Among the 2799 patients who received intravenous pembrolizumab, 41% were exposed for 6 months or more and 21% were exposed for 12 months or more.

The most common adverse reactions (≥20%) in patients who received KEYTRUDA QLEX in combination with chemotherapy were nausea (25%), fatigue (25%), and musculoskeletal pain (21%).

The safety of KEYTRUDA QLEX for the approved indications is also based on the safety of intravenous pembrolizumab given as a single agent or in combination with other antitumor medicines.

The most common adverse reactions (≥20%) in patients who received intravenous pembrolizumab were:

- as a single agent: fatigue, musculoskeletal pain, rash, diarrhea, pyrexia, cough, decreased appetite, pruritus, dyspnea, constipation, pain, abdominal pain, nausea, and hypothyroidism.
- in combination with chemotherapy or chemoradiotherapy: fatigue/asthenia, nausea, constipation, diarrhea, decreased appetite, rash, vomiting, cough, dyspnea, pyrexia, alopecia, peripheral neuropathy, mucosal inflammation, stomatitis, headache, weight loss, abdominal pain, arthralgia, myalgia, insomnia, palmar-plantar erythrodysesthesia, urinary tract infection, hypothyroidism, radiation skin injury, dysphagia, dry mouth, and musculoskeletal pain.
- in combination with chemotherapy and bevacizumab: peripheral neuropathy, alopecia, anemia, fatigue/asthenia, nausea, neutropenia, diarrhea, hypertension, thrombocytopenia, constipation, arthralgia, vomiting, urinary tract infection, rash, leukopenia, hypothyroidism, decreased appetite, pyrexia, epistaxis, decreased white blood cell count, and stomatitis.
- in combination with axitinib: diarrhea, fatigue/asthenia, hypertension, hepatotoxicity, hypothyroidism, decreased appetite, palmar-plantar erythrodysesthesia, nausea, stomatitis/mucosal inflammation, dysphonia, rash, cough, and constipation.
- in combination with lenvatinib: hypothyroidism, hypertension, fatigue, diarrhea, musculoskeletal disorders, nausea, decreased appetite, vomiting, stomatitis, weight loss, abdominal pain, urinary tract infection, proteinuria, constipation, headache, hemorrhagic events, palmar-plantar erythrodysesthesia, dysphonia, rash, hepatotoxicity, and acute kidney injury.
- in combination with enfortumab vedotin: rash, peripheral neuropathy, fatigue, pruritus, diarrhea, alopecia, weight loss, decreased appetite, dry eye, nausea, constipation, dysgeusia, and urinary tract infection.

Adverse Reactions in Patients with NSCLC Treated with KEYTRUDA QLEX

The safety of KEYTRUDA QLEX compared to intravenous pembrolizumab in patients with previously untreated, metastatic NSCLC with no EGFR, ALK or ROS1 genomic tumor aberrations was evaluated in Study MK-3475A-D77 [see Clinical Studies (14.1)]. A total of 377 patients received either KEYTRUDA QLEX 790 mg/9,600 units every 6 weeks in combination with platinum doublet chemotherapy (n=251) or intravenous pembrolizumab 400 mg every 6 weeks in combination with platinum doublet chemotherapy (n=126).

Among patients who received KEYTRUDA QLEX, 58% were exposed for 6 months or longer and 3.2% were exposed for greater than one year.

The median age of patients who received KEYTRUDA QLEX was 65 years (range: 39 to 87); 73% male, 63% White; 29% Asian, 4.8% multiple races, 2% Black or African American, 0.8% Alaska Native or American Indian; and 29% were of Hispanic or Latino ethnicity.

Serious adverse reactions occurred in 39% of patients who received KEYTRUDA QLEX in combination with chemotherapy. Serious adverse reactions in ≥1% of patients who received KEYTRUDA QLEX were pneumonia (10%), thrombocytopenia (4%), febrile neutropenia (4%), neutropenia (2.8%), musculoskeletal pain (2%), pneumonitis (2%), diarrhea (1.6%), rash (1.2%), respiratory failure (1.2%), and anemia (1.2%). Fatal adverse reactions occurred in 10% of patients who received KEYTRUDA QLEX in combination with chemotherapy including pneumonia (3.2%), neutropenic sepsis (2%), death not otherwise specified (1.6%), respiratory failure (1.2%), parotitis (0.4%), pneumonitis (0.4%), pneumothorax (0.4%), pulmonary embolism (0.4%), neutropenic colitis (0.4%), and seizure (0.4%).

Permanent discontinuation of KEYTRUDA QLEX due to an adverse reaction occurred in 16% of patients. Adverse reactions which resulted in permanent discontinuation of KEYTRUDA QLEX in ≥2% of patients included pneumonia and pneumonitis.

Dosage interruptions of KEYTRUDA QLEX due to an adverse reaction occurred in 45% of patients. Adverse reactions which required dosage interruption in ≥2% of patients included neutropenia, anemia, thrombocytopenia, pneumonia, rash, and increased aspartate aminotransferase.

Tables 4 and 5 summarize the adverse reactions and laboratory abnormalities, respectively, in patients on KEYTRUDA QLEX in Study MK-3475A-D77.

Table 4: Adverse Reactions Occurring in ≥10% of Patients with Metastatic NSCLC Receiving KEYTRUDA QLEX in Study MK-3475A-D77
Adverse Reaction | KEYTRUDA QLEX and Platinum Doublet Chemotherapy |  | Intravenous Pembrolizumab and Platinum Doublet Chemotherapy
Adverse Reaction | (n=251) |  | (n=126)
Adverse Reaction | All Grades [Graded per NCI CTCAE V5.0] (%) | Grades 3-4 (%) | All Grades (%) | Grades 3-4 (%)
Gastrointestinal
Nausea | 25 | 1.2 | 25 | 0.8
Diarrhea [Includes diarrhea, colitis, and enterocolitis.] | 16 | 2 | 14 | 0.8
Constipation | 14 | 0 | 18 | 1.6
General
Fatigue [Includes fatigue, asthenia.] | 25 | 3.6 | 26 | 3.2
Musculoskeletal and Connective Tissue
Musculoskeletal pain [Includes musculoskeletal pain, arthralgia, arthritis, back pain, bone pain, musculoskeletal chest pain, musculoskeletal stiffness, myalgia, non-cardiac chest pain, and pain in extremity.] | 21 | 2.4 | 30 | 2.4
Skin and Subcutaneous Tissue
Rash [Includes rash, dermatitis, dermatitis acneiform, dermatitis bullous, dermatitis exfoliative, eczema, erythema multiforme, immune-mediated dermatitis, rash erythematous, rash follicular, rash generalized, rash macular, rash maculo-papular, rash papular, rash pruritic, and skin exfoliation.] | 18 | 2 | 19 | 0.8
Pruritus | 12 | 0 | 13 | 0.8
Endocrine
Hypothyroidism | 14 | 0 | 12 | 0
Infections
Pneumonia [Includes pneumonia, COVID-19 pneumonia, lower respiratory tract infection, lung abscess, pneumocystis jirovecii pneumonia, pneumonia bacterial, and pneumonia mycoplasmal.] | 17 | 10 | 16 | 7
Nervous System
Peripheral neuropathy [Includes neuropathy peripheral, hypoaesthesia, neuralgia, paraesthesia, and peripheral sensory neuropathy.] | 11 | 0.4 | 14 | 0
Metabolism and Nutrition
Decreased appetite | 11 | 0.8 | 21 | 2.4
Hyperglycemia | 11 | 0.8 | 11 | 0.8
Respiratory, Thoracic and Mediastinal
Cough [Includes cough, productive cough, and upper-airway cough syndrome.] | 10 | 0 | 11 | 0.8

Clinically relevant adverse reactions in <10% of patients who received KEYTRUDA QLEX included local injection site reactions (2.4%).

Table 5: Laboratory Abnormalities Worsened from Baseline Occurring in ≥20% of Patients with Metastatic NSCLC Receiving KEYTRUDA QLEX in Study MK-3475A-D77
Laboratory Test [Each test incidence is based on the number of patients who had both baseline and at least one on-study laboratory measurement available: KEYTRUDA QLEX plus platinum doublet chemotherapy (range: 240 to 246 patients) and intravenous pembrolizumab plus platinum doublet chemotherapy (range: 124 to 125 patients).] | KEYTRUDA QLEX and Platinum Doublet Chemotherapy |  | Intravenous Pembrolizumab and Platinum Doublet Chemotherapy
Laboratory Test [Each test incidence is based on the number of patients who had both baseline and at least one on-study laboratory measurement available: KEYTRUDA QLEX plus platinum doublet chemotherapy (range: 240 to 246 patients) and intravenous pembrolizumab plus platinum doublet chemotherapy (range: 124 to 125 patients).] | All Grades [Graded per NCI CTCAE V5.0] (%) | Grades 3-4 (%) | All Grades (%) | Grades 3-4 (%)
Hematology
Anemia | 80 | 22 | 86 | 26
Leukopenia | 61 | 13 | 52 | 10
Neutropenia | 58 | 28 | 49 | 19
Lymphopenia | 55 | 22 | 54 | 18
Thrombocytopenia | 43 | 11 | 41 | 6
Chemistry
Increased AST | 43 | 2.5 | 38 | 3.2
Hypoalbuminemia | 38 | 0.4 | 39 | 0
Increased ALT | 37 | 2.1 | 36 | 0.8
Hyponatremia | 35 | 4.1 | 42 | 7
Increased creatinine | 33 | 4.5 | 38 | 6
Hypocalcemia | 31 | 2.1 | 31 | 2.4
Increased alkaline phosphatase | 29 | 0.4 | 34 | 0
Hypokalemia | 21 | 5 | 24 | 6

Adverse Reactions in Adult and Pediatric Patients Treated with Intravenous Pembrolizumab

The safety of KEYTRUDA QLEX for its approved indications [see Indications and Usage (1)] has been established in adequate and well-controlled studies of KEYTRUDA QLEX in combination with platinum doublet chemotherapy (Study MK-3475A-D77) and intravenous pembrolizumab, as a single agent or in combination therapy, across tumor types.

Below is a description of adverse reactions of intravenous pembrolizumab in these adequate and well-controlled studies.

Melanoma

Ipilimumab-Naive Melanoma

The safety of intravenous pembrolizumab for the treatment of patients with unresectable or metastatic melanoma who had not received prior ipilimumab and who had received no more than one prior systemic therapy was investigated in KEYNOTE-006. KEYNOTE-006 was a multicenter, open-label, active-controlled trial where patients were randomized (1:1:1) and received intravenous pembrolizumab 10 mg/kg every 2 weeks (n=278) or intravenous pembrolizumab 10 mg/kg every 3 weeks (n=277) until disease progression or unacceptable toxicity or ipilimumab 3 mg/kg every 3 weeks for 4 doses unless discontinued earlier for disease progression or unacceptable toxicity (n=256) [see Clinical Studies (14.2)]. Patients with autoimmune disease, a medical condition that required systemic corticosteroids or other immunosuppressive medication; a history of interstitial lung disease; or active infection requiring therapy, including HIV or hepatitis B or C, were ineligible.

The median duration of exposure was 5.6 months (range: 1 day to 11.0 months) for intravenous pembrolizumab and similar in both treatment arms. Fifty-one and 46% of patients received intravenous pembrolizumab 10 mg/kg every 2 or 3 weeks, respectively, for ≥6 months. No patients in either arm received treatment for more than one year.

The study population characteristics were: median age of 62 years (range: 18 to 89); 60% male; 98% White; 32% had an elevated lactate dehydrogenase (LDH) value at baseline; 65% had M1c stage disease; 9% with history of brain metastasis; and approximately 36% had been previously treated with systemic therapy which included a BRAF inhibitor (15%), chemotherapy (13%), and immunotherapy (6%).

In KEYNOTE-006, the adverse reaction profile was similar for the every 2 week and every 3 week schedule, therefore summary safety results are provided in a pooled analysis (n=555) of both intravenous pembrolizumab arms. Adverse reactions leading to permanent discontinuation of intravenous pembrolizumab occurred in 9% of patients. Adverse reactions leading to discontinuation of intravenous pembrolizumab in more than one patient were colitis (1.4%), autoimmune hepatitis (0.7%), allergic reaction (0.4%), polyneuropathy (0.4%), and cardiac failure (0.4%). Adverse reactions leading to interruption of intravenous pembrolizumab occurred in 21% of patients; the most common (≥1%) was diarrhea (2.5%). Tables 6 and 7 summarize selected adverse reactions and laboratory abnormalities, respectively, in patients on intravenous pembrolizumab in KEYNOTE-006.

Table 6: Selected [Adverse reactions occurring at same or higher incidence than in the ipilimumab arm] Adverse Reactions Occurring in ≥10% of Patients Receiving Intravenous Pembrolizumab in KEYNOTE-006
Adverse Reaction | Intravenous Pembrolizumab 10 mg/kg every 2 or 3 weeks |  | Ipilimumab
Adverse Reaction | n=555 |  | n=256
 | All Grades [Graded per NCI CTCAE v4.0] (%) | Grades 3-4 (%) | All Grades (%) | Grades 3-4 (%)
General
Fatigue | 28 | 0.9 | 28 | 3.1
Skin and Subcutaneous Tissue
Rash [Includes rash, rash erythematous, rash follicular, rash generalized, rash macular, rash maculo-papular, rash papular, rash pruritic, and exfoliative rash.] | 24 | 0.2 | 23 | 1.2
Vitiligo [Includes skin hypopigmentation] | 13 | 0 | 2 | 0
Musculoskeletal and Connective Tissue
Arthralgia | 18 | 0.4 | 10 | 1.2
Back pain | 12 | 0.9 | 7 | 0.8
Respiratory, Thoracic and Mediastinal
Cough | 17 | 0 | 7 | 0.4
Dyspnea | 11 | 0.9 | 7 | 0.8
Metabolism and Nutrition
Decreased appetite | 16 | 0.5 | 14 | 0.8
Nervous System
Headache | 14 | 0.2 | 14 | 0.8

Other clinically important adverse reactions occurring in ≥10% of patients receiving intravenous pembrolizumab were diarrhea (26%), nausea (21%), and pruritus (17%).

Table 7: Selected [Laboratory abnormalities occurring at same or higher incidence than in ipilimumab arm] Laboratory Abnormalities Worsened from Baseline Occurring in ≥20% of Melanoma Patients Receiving Intravenous Pembrolizumab in KEYNOTE-006
Laboratory Test [Each test incidence is based on the number of patients who had both baseline and at least one on-study laboratory measurement available: intravenous pembrolizumab (520 to 546 patients) and ipilimumab (237 to 247 patients); hypertriglyceridemia: intravenous pembrolizumab n=429 and ipilimumab n=183; hypercholesterolemia: intravenous pembrolizumab n=484 and ipilimumab n=205.] | Intravenous Pembrolizumab 10 mg/kg every 2 or 3 weeks |  | Ipilimumab
Laboratory Test [Each test incidence is based on the number of patients who had both baseline and at least one on-study laboratory measurement available: intravenous pembrolizumab (520 to 546 patients) and ipilimumab (237 to 247 patients); hypertriglyceridemia: intravenous pembrolizumab n=429 and ipilimumab n=183; hypercholesterolemia: intravenous pembrolizumab n=484 and ipilimumab n=205.] | All Grades [Graded per NCI CTCAE v4.0] % | Grades 3-4 % | All Grades % | Grades 3-4 %
Chemistry
Hyperglycemia | 45 | 4.2 | 45 | 3.8
Hypertriglyceridemia | 43 | 2.6 | 31 | 1.1
Hyponatremia | 28 | 4.6 | 26 | 7
Increased AST | 27 | 2.6 | 25 | 2.5
Hypercholesterolemia | 20 | 1.2 | 13 | 0
Hematology
Anemia | 35 | 3.8 | 33 | 4.0
Lymphopenia | 33 | 7 | 25 | 6

Other laboratory abnormalities occurring in ≥20% of patients receiving intravenous pembrolizumab were increased hypoalbuminemia (27% all Grades; 2.4% Grades 3-4), increased ALT (23% all Grades; 3.1% Grades 3-4), and increased alkaline phosphatase (21% all Grades, 2% Grades 3-4).

Ipilimumab-Refractory Melanoma

The safety of intravenous pembrolizumab in patients with unresectable or metastatic melanoma with disease progression following ipilimumab and, if BRAF V600 mutation positive, a BRAF inhibitor, was investigated in KEYNOTE-002. KEYNOTE-002 was a multicenter, partially blinded (intravenous pembrolizumab dose), randomized (1:1:1), active-controlled trial in which 528 patients received intravenous pembrolizumab 2 mg/kg (n=178) or 10 mg/kg (n=179) every 3 weeks or investigator's choice of chemotherapy (n=171), consisting of dacarbazine (26%), temozolomide (25%), paclitaxel and carboplatin (25%), paclitaxel (16%), or carboplatin (8%) [see Clinical Studies (14.2)]. Patients with autoimmune disease, severe immune-related toxicity related to ipilimumab, defined as any Grade 4 toxicity or Grade 3 toxicity requiring corticosteroid treatment (greater than 10 mg/day prednisone or equivalent dose) for greater than 12 weeks; medical conditions that required systemic corticosteroids or other immunosuppressive medication; a history of interstitial lung disease; or an active infection requiring therapy, including HIV or hepatitis B or C, were ineligible.

The median duration of exposure to intravenous pembrolizumab 2 mg/kg every 3 weeks was 3.7 months (range: 1 day to 16.6 months) and to intravenous pembrolizumab 10 mg/kg every 3 weeks was 4.8 months (range: 1 day to 16.8 months). In the intravenous pembrolizumab 2 mg/kg arm, 36% of patients were exposed to intravenous pembrolizumab for ≥6 months and 4% were exposed for ≥12 months. In the 10 mg/kg arm, 41% of patients were exposed to intravenous pembrolizumab for ≥6 months and 6% of patients were exposed to intravenous pembrolizumab for ≥12 months.

The study population characteristics were: median age of 62 years (range: 15 to 89); 61% male; 98% White; 41% had an elevated LDH value at baseline; 83% had M1c stage disease; 73% received two or more prior therapies for advanced or metastatic disease (100% received ipilimumab and 25% a BRAF inhibitor); and 15% with history of brain metastasis.

In KEYNOTE-002, the adverse reaction profile was similar for the 2 mg/kg dose and 10 mg/kg dose, therefore summary safety results are provided in a pooled analysis (n=357) of both intravenous pembrolizumab arms. Adverse reactions resulting in permanent discontinuation occurred in 12% of patients receiving intravenous pembrolizumab; the most common (≥1%) were general physical health deterioration (1%), asthenia (1%), dyspnea (1%), pneumonitis (1%), and generalized edema (1%). Adverse reactions leading to interruption of intravenous pembrolizumab occurred in 14% of patients; the most common (≥1%) were dyspnea (1%), diarrhea (1%), and maculo-papular rash (1%). Tables 8 and 9 summarize adverse reactions and laboratory abnormalities, respectively, in patients on intravenous pembrolizumab in KEYNOTE-002.

Table 8: Selected [Adverse reactions occurring at same or higher incidence than in chemotherapy arm] Adverse Reactions Occurring in ≥10% of Patients Receiving Intravenous Pembrolizumab in KEYNOTE-002
Adverse Reaction | Intravenous Pembrolizumab 2 mg/kg or 10 mg/kg every 3 weeks |  | Chemotherapy [Chemotherapy: dacarbazine, temozolomide, carboplatin plus paclitaxel, paclitaxel, or carboplatin]
Adverse Reaction | n=357 |  | n=171
 | All Grades [Graded per NCI CTCAE v4.0] (%) | Grades 3-4 (%) | All Grades (%) | Grades 3-4 (%)
Skin and Subcutaneous Tissue
Pruritus | 28 | 0 | 8 | 0
Rash [Includes rash, rash erythematous, rash generalized, rash macular, rash maculo-papular, rash papular, and rash pruritic] | 24 | 0.6 | 8 | 0
Gastrointestinal
Constipation | 22 | 0.3 | 20 | 2.3
Diarrhea | 20 | 0.8 | 20 | 2.3
Abdominal pain | 13 | 1.7 | 8 | 1.2
Respiratory, Thoracic and Mediastinal
Cough | 18 | 0 | 16 | 0
General
Pyrexia | 14 | 0.3 | 9 | 0.6
Asthenia | 10 | 2.0 | 9 | 1.8
Musculoskeletal and Connective Tissue
Arthralgia | 14 | 0.6 | 10 | 1.2

Other clinically important adverse reactions occurring in patients receiving intravenous pembrolizumab were fatigue (43%), nausea (22%), decreased appetite (20%), vomiting (13%), and peripheral neuropathy (1.7%).

Table 9: Selected [Laboratory abnormalities occurring at same or higher incidence than in chemotherapy arm.] Laboratory Abnormalities Worsened from Baseline Occurring in ≥20% of Melanoma Patients Receiving Intravenous Pembrolizumab in KEYNOTE-002
Laboratory Test [Each test incidence is based on the number of patients who had both baseline and at least one on-study laboratory measurement available: intravenous pembrolizumab (range: 320 to 325 patients) and chemotherapy (range: 154 to 161 patients); hypertriglyceridemia: intravenous pembrolizumab n=247 and chemotherapy n=116; decreased bicarbonate: intravenous pembrolizumab n=263 and chemotherapy n=123.] | Intravenous Pembrolizumab 2 mg/kg or 10 mg/kg every 3 weeks |  | Chemotherapy
 | All Grades [Graded per NCI CTCAE v4.0] % | Grades 3-4 % | All Grades % | Grades 3-4 %
Chemistry
Hyperglycemia | 49 | 6 | 44 | 6
Hypoalbuminemia | 37 | 1.9 | 33 | 0.6
Hyponatremia | 37 | 7 | 24 | 3.8
Hypertriglyceridemia | 33 | 0 | 32 | 0.9
Increased alkaline phosphatase | 26 | 3.1 | 18 | 1.9
Increased AST | 24 | 2.2 | 16 | 0.6
Decreased bicarbonate | 22 | 0.4 | 13 | 0
Hypocalcemia | 21 | 0.3 | 18 | 1.9
Increased ALT | 21 | 1.8 | 16 | 0.6

Other laboratory abnormalities occurring in ≥20% of patients receiving intravenous pembrolizumab were anemia (44% all Grades; 10% Grades 3-4) and lymphopenia (40% all Grades; 9% Grades 3-4).

Adjuvant Treatment of Resected Stage IIB or IIC Melanoma

Among the 969 patients with Stage IIB or IIC melanoma enrolled in KEYNOTE-716 [see Clinical Studies (14.2)] treated with intravenous pembrolizumab, the median duration of exposure to intravenous pembrolizumab was 9.9 months (range: 0 to 15.4 months). Patients with autoimmune disease or a medical condition that required immunosuppression or mucosal or ocular melanoma were ineligible. Adverse reactions occurring in patients with Stage IIB or IIC melanoma were similar to those occurring in 1011 patients with Stage III melanoma from KEYNOTE-054 or the 2799 patients with melanoma or NSCLC treated with intravenous pembrolizumab as a single agent.

Adjuvant Treatment of Stage III Resected Melanoma

The safety of intravenous pembrolizumab as a single agent was investigated in KEYNOTE-054, a randomized (1:1) double-blind trial in which 1019 patients with completely resected Stage IIIA (>1 mm lymph node metastasis), IIIB or IIIC melanoma received 200 mg of intravenous pembrolizumab by intravenous infusion every 3 weeks (n=509) or placebo (n=502) for up to one year [see Clinical Studies (14.2)]. Patients with active autoimmune disease or a medical condition that required immunosuppression or mucosal or ocular melanoma were ineligible. Seventy-six percent of patients received intravenous pembrolizumab for 6 months or longer.

The study population characteristics were: median age of 54 years (range: 19 to 88), 25% age 65 or older; 62% male; and 94% ECOG PS of 0 and 6% ECOG PS of 1. Sixteen percent had Stage IIIA, 46% had Stage IIIB, 18% had Stage IIIC (1-3 positive lymph nodes), and 20% had Stage IIIC (≥4 positive lymph nodes).

Two patients treated with intravenous pembrolizumab died from causes other than disease progression; causes of death were drug reaction with eosinophilia and systemic symptoms and autoimmune myositis with respiratory failure. Serious adverse reactions occurred in 25% of patients receiving intravenous pembrolizumab. Adverse reactions leading to permanent discontinuation occurred in 14% of patients receiving intravenous pembrolizumab; the most common (≥1%) were pneumonitis (1.4%), colitis (1.2%), and diarrhea (1%). Adverse reactions leading to interruption of intravenous pembrolizumab occurred in 19% of patients; the most common (≥1%) were diarrhea (2.4%), pneumonitis (2%), increased ALT (1.4%), arthralgia (1.4%), increased AST (1.4%), dyspnea (1%), and fatigue (1%). Tables 10 and 11 summarize adverse reactions and laboratory abnormalities, respectively, in patients on intravenous pembrolizumab in KEYNOTE-054.

Table 10: Selected [Adverse reactions occurring at same or higher incidence than in placebo arm] Adverse Reactions Occurring in ≥10% of Patients Receiving Intravenous Pembrolizumab in KEYNOTE-054
Adverse Reaction | Intravenous Pembrolizumab 200 mg every 3 weeks n=509 |  | Placebo n=502
Adverse Reaction | All Grades [Graded per NCI CTCAE v4.03] (%) | Grades 3-4 (%) | All Grades (%) | Grades 3-4 (%)
Gastrointestinal
Diarrhea | 28 | 1.2 | 26 | 1.2
Nausea | 17 | 0.2 | 15 | 0
Skin and Subcutaneous Tissue
Pruritus | 19 | 0 | 12 | 0
Rash | 13 | 0.2 | 9 | 0
Musculoskeletal and Connective Tissue
Arthralgia | 16 | 1.2 | 14 | 0
Endocrine
Hypothyroidism | 15 | 0 | 2.8 | 0
Hyperthyroidism | 10 | 0.2 | 1.2 | 0
Respiratory, Thoracic and Mediastinal
Cough | 14 | 0 | 11 | 0
General
Asthenia | 11 | 0.2 | 8 | 0
Influenza like illness | 11 | 0 | 8 | 0
Investigations
Weight loss | 11 | 0 | 8 | 0

Table 11: Selected [Laboratory abnormalities occurring at same or higher incidence than placebo.] Laboratory Abnormalities Worsened from Baseline Occurring in ≥20% of Melanoma Patients Receiving Intravenous Pembrolizumab in KEYNOTE-054
Laboratory Test [Each test incidence is based on the number of patients who had both baseline and at least one on-study laboratory measurement available: intravenous pembrolizumab (range: 502 to 505 patients) and placebo (range: 491 to 497 patients).] | Intravenous Pembrolizumab 200 mg every 3 weeks |  | Placebo
Laboratory Test [Each test incidence is based on the number of patients who had both baseline and at least one on-study laboratory measurement available: intravenous pembrolizumab (range: 502 to 505 patients) and placebo (range: 491 to 497 patients).] | All Grades [Graded per NCI CTCAE v4.03] % | Grades 3-4 % | All Grades % | Grades 3-4 %
Chemistry
Increased ALT | 25 | 2.4 | 15 | 0.2
Increased AST | 22 | 1.8 | 14 | 0.4
Hematology
Lymphopenia | 22 | 1 | 15 | 1.2

NSCLC

First-line treatment of metastatic nonsquamous NSCLC with pemetrexed and platinum chemotherapy

The safety of intravenous pembrolizumab in combination with pemetrexed and investigator's choice of platinum (either carboplatin or cisplatin) was investigated in KEYNOTE-189, a multicenter, double-blind, randomized (2:1), active-controlled trial in patients with previously untreated, metastatic nonsquamous NSCLC with no EGFR or ALK genomic tumor aberrations [see Clinical Studies (14.3)]. A total of 607 patients received intravenous pembrolizumab 200 mg, pemetrexed and platinum every 3 weeks for 4 cycles followed by intravenous pembrolizumab and pemetrexed (n=405) or placebo, pemetrexed, and platinum every 3 weeks for 4 cycles followed by placebo and pemetrexed (n=202). Patients with autoimmune disease that required systemic therapy within 2 years of treatment; a medical condition that required immunosuppression; or who had received more than 30 Gy of thoracic radiation within the prior 26 weeks were ineligible.

The median duration of exposure to intravenous pembrolizumab 200 mg every 3 weeks was 7.2 months (range: 1 day to 20.1 months). Sixty percent of patients in the intravenous pembrolizumab arm were exposed to intravenous pembrolizumab for ≥6 months. Seventy-two percent of patients received carboplatin.

The study population characteristics were: median age of 64 years (range: 34 to 84), 49% age 65 or older; 59% male; 94% White and 3% Asian; and 18% with history of brain metastases at baseline.

Intravenous pembrolizumab was discontinued for adverse reactions in 20% of patients. The most common adverse reactions resulting in permanent discontinuation of intravenous pembrolizumab were pneumonitis (3%) and acute kidney injury (2%). Adverse reactions leading to the interruption of intravenous pembrolizumab occurred in 53% of patients; the most common adverse reactions or laboratory abnormalities leading to interruption of intravenous pembrolizumab (≥2%) were neutropenia (13%), asthenia/fatigue (7%), anemia (7%), thrombocytopenia (5%), diarrhea (4%), pneumonia (4%), increased blood creatinine (3%), dyspnea (2%), febrile neutropenia (2%), upper respiratory tract infection (2%), increased ALT (2%), and pyrexia (2%). Tables 12 and 13 summarize adverse reactions and laboratory abnormalities, respectively, in patients on intravenous pembrolizumab in KEYNOTE-189.

Table 12: Adverse Reactions Occurring in ≥20% of Patients in KEYNOTE-189
Adverse Reaction | Intravenous Pembrolizumab 200 mg every 3 weeks Pemetrexed Platinum Chemotherapy n=405 |  | Placebo Pemetrexed Platinum Chemotherapy n=202
 | All Grades [Graded per NCI CTCAE v4.03] (%) | Grades 3-4 (%) | All Grades (%) | Grades 3-4 (%)
Gastrointestinal
Nausea | 56 | 3.5 | 52 | 3.5
Constipation | 35 | 1.0 | 32 | 0.5
Diarrhea | 31 | 5 | 21 | 3.0
Vomiting | 24 | 3.7 | 23 | 3.0
General
Fatigue [Includes asthenia and fatigue] | 56 | 12 | 58 | 6
Pyrexia | 20 | 0.2 | 15 | 0
Metabolism and Nutrition
Decreased appetite | 28 | 1.5 | 30 | 0.5
Skin and Subcutaneous Tissue
Rash [Includes genital rash, rash, rash generalized, rash macular, rash maculo-papular, rash papular, rash pruritic, and rash pustular.] | 25 | 2.0 | 17 | 2.5
Respiratory, Thoracic and Mediastinal
Cough | 21 | 0 | 28 | 0
Dyspnea | 21 | 3.7 | 26 | 5

Table 13: Laboratory Abnormalities Worsened from Baseline Occurring in ≥20% of Patients in KEYNOTE-189
Laboratory Test [Each test incidence is based on the number of patients who had both baseline and at least one on-study laboratory measurement available: intravenous pembrolizumab /pemetrexed/platinum chemotherapy (range: 381 to 401 patients) and placebo/pemetrexed/platinum chemotherapy (range: 184 to 197 patients).] | Intravenous Pembrolizumab 200 mg every 3 weeks Pemetrexed Platinum Chemotherapy |  | Placebo Pemetrexed Platinum Chemotherapy
 | All Grades [Graded per NCI CTCAE v4.03] % | Grades 3-4 % | All Grades % | Grades 3-4 %
Hematology
Anemia | 85 | 17 | 81 | 18
Lymphopenia | 65 | 22 | 64 | 25
Neutropenia | 50 | 21 | 41 | 19
Thrombocytopenia | 30 | 12 | 29 | 8
Chemistry
Hyperglycemia | 63 | 9 | 60 | 7
Increased ALT | 47 | 3.8 | 42 | 2.6
Increased AST | 47 | 2.8 | 40 | 1.0
Hypoalbuminemia | 39 | 2.8 | 39 | 1.1
Increased creatinine | 37 | 4.2 | 25 | 1.0
Hyponatremia | 32 | 7 | 23 | 6
Hypophosphatemia | 30 | 10 | 28 | 14
Increased alkaline phosphatase | 26 | 1.8 | 29 | 2.1
Hypocalcemia | 24 | 2.8 | 17 | 0.5
Hyperkalemia | 24 | 2.8 | 19 | 3.1
Hypokalemia | 21 | 5 | 20 | 5

First-line treatment of metastatic squamous NSCLC with carboplatin and either paclitaxel or paclitaxel protein-bound chemotherapy

The safety of intravenous pembrolizumab in combination with carboplatin and investigator's choice of either paclitaxel or paclitaxel protein-bound was investigated in KEYNOTE-407, a multicenter, double-blind, randomized (1:1), placebo-controlled trial in 558 patients with previously untreated, metastatic squamous NSCLC [see Clinical Studies (14.3)]. Safety data are available for the first 203 patients who received intravenous pembrolizumab and chemotherapy (n=101) or placebo and chemotherapy (n=102). Patients with autoimmune disease that required systemic therapy within 2 years of treatment; a medical condition that required immunosuppression; or who had received more than 30 Gy of thoracic radiation within the prior 26 weeks were ineligible.

The median duration of exposure to intravenous pembrolizumab was 7 months (range: 1 day to 12 months). Sixty-one percent of patients in the intravenous pembrolizumab arm were exposed to intravenous pembrolizumab for ≥6 months. A total of 139 of 203 patients (68%) received paclitaxel and 64 patients (32%) received paclitaxel protein-bound in combination with carboplatin.

The study population characteristics were: median age of 65 years (range: 40 to 83), 52% age 65 or older; 78% male; 83% White; and 9% with history of brain metastases.

Intravenous pembrolizumab was discontinued for adverse reactions in 15% of patients, with no single type of adverse reaction accounting for the majority. Adverse reactions leading to interruption of intravenous pembrolizumab occurred in 43% of patients; the most common (≥2%) were thrombocytopenia (20%), neutropenia (11%), anemia (6%), asthenia (2%), and diarrhea (2%). The most frequent (≥2%) serious adverse reactions were febrile neutropenia (6%), pneumonia (6%), and urinary tract infection (3%).

The adverse reactions observed in KEYNOTE-407 were similar to those observed in KEYNOTE-189 with the exception that increased incidences of alopecia (47% vs. 36%) and peripheral neuropathy (31% vs. 25%) were observed in the intravenous pembrolizumab and chemotherapy arm compared to the placebo and chemotherapy arm in KEYNOTE-407.

Previously Untreated NSCLC

The safety of intravenous pembrolizumab was investigated in KEYNOTE-042, a multicenter, open-label, randomized (1:1), active-controlled trial in 1251 patients with PD-L1 expressing, previously untreated Stage III NSCLC who were not candidates for surgical resection or definitive chemoradiation or metastatic NSCLC [see Clinical Studies (14.3)]. Patients received intravenous pembrolizumab 200 mg every 3 weeks (n=636) or investigator's choice of chemotherapy (n=615), consisting of pemetrexed and carboplatin followed by optional pemetrexed (n=312) or paclitaxel and carboplatin followed by optional pemetrexed (n=303) every 3 weeks. Patients with EGFR or ALK genomic tumor aberrations; autoimmune disease that required systemic therapy within 2 years of treatment; a medical condition that required immunosuppression; or who had received more than 30 Gy of thoracic radiation within the prior 26 weeks were ineligible.

The median duration of exposure to intravenous pembrolizumab was 5.6 months (range: 1 day to 27.3 months). Forty-eight percent of patients in the intravenous pembrolizumab arm were exposed to intravenous pembrolizumab 200 mg for ≥6 months.

The study population characteristics were: median age of 63 years (range: 25 to 90), 45% age 65 or older; 71% male; and 64% White, 30% Asian, and 2% Black. Nineteen percent were Hispanic or Latino. Eighty-seven percent had metastatic disease (Stage IV), 13% had Stage III disease (2% Stage IIIA and 11% Stage IIIB), and 5% had treated brain metastases at baseline.

Intravenous pembrolizumab was discontinued for adverse reactions in 19% of patients. The most common adverse reactions resulting in permanent discontinuation of intravenous pembrolizumab were pneumonitis (3.0%), death due to unknown cause (1.6%), and pneumonia (1.4%). Adverse reactions leading to interruption of intravenous pembrolizumab occurred in 33% of patients; the most common adverse reactions or laboratory abnormalities leading to interruption of intravenous pembrolizumab (≥2%) were pneumonitis (3.1%), pneumonia (3.0%), hypothyroidism (2.2%), and increased ALT (2.0%). The most frequent (≥2%) serious adverse reactions were pneumonia (7%), pneumonitis (3.9%), pulmonary embolism (2.4%), and pleural effusion (2.2%).

Tables 14 and 15 summarize the adverse reactions and laboratory abnormalities, respectively, in patients treated with intravenous pembrolizumab in KEYNOTE-042.

Table 14: Adverse Reactions Occurring in ≥10% of Patients in KEYNOTE-042
Adverse Reaction | Intravenous Pembrolizumab 200 mg every 3 weeks n=636 |  | Chemotherapy n=615
Adverse Reaction | All Grades [Graded per NCI CTCAE v4.03] (%) | Grades 3-5 (%) | All Grades (%) | Grades 3-5 (%)
General
Fatigue [Includes fatigue and asthenia] | 25 | 3.1 | 33 | 3.9
Pyrexia | 10 | 0.3 | 8 | 0
Metabolism and Nutrition
Decreased appetite | 17 | 1.7 | 21 | 1.5
Respiratory, Thoracic and Mediastinal
Dyspnea | 17 | 2.0 | 11 | 0.8
Cough | 16 | 0.2 | 11 | 0.3
Skin and Subcutaneous Tissue
Rash [Includes rash, rash generalized, rash macular, rash maculo-papular, rash papular, rash pruritic, and rash pustular.] | 15 | 1.3 | 8 | 0.2
Gastrointestinal
Constipation | 12 | 0 | 21 | 0.2
Diarrhea | 12 | 0.8 | 12 | 0.5
Nausea | 12 | 0.5 | 32 | 1.1
Endocrine
Hypothyroidism | 12 | 0.2 | 1.5 | 0
Infections
Pneumonia | 12 | 7 | 9 | 6
Investigations
Weight loss | 10 | 0.9 | 7 | 0.2

Table 15: Laboratory Abnormalities Worsened from Baseline in ≥20% of Patients in KEYNOTE-042
Laboratory Test [Each test incidence is based on the number of patients who had both baseline and at least one on-study laboratory measurement available: intravenous pembrolizumab (range: 598 to 610 patients) and chemotherapy (range: 585 to 598 patients); increased prothrombin INR: intravenous pembrolizumab n=203 and chemotherapy n=173.] | Intravenous Pembrolizumab 200 mg every 3 weeks |  | Chemotherapy
Laboratory Test [Each test incidence is based on the number of patients who had both baseline and at least one on-study laboratory measurement available: intravenous pembrolizumab (range: 598 to 610 patients) and chemotherapy (range: 585 to 598 patients); increased prothrombin INR: intravenous pembrolizumab n=203 and chemotherapy n=173.] | All Grades [Graded per NCI CTCAE v4.03] % | Grades 3-4 % | All Grades % | Grades 3-4 %
Chemistry
Hyperglycemia | 52 | 4.7 | 51 | 5
Increased ALT | 33 | 4.8 | 34 | 2.9
Hypoalbuminemia | 33 | 2.2 | 29 | 1.0
Increased AST | 31 | 3.6 | 32 | 1.7
Hyponatremia | 31 | 9 | 32 | 8
Increased alkaline phosphatase | 29 | 2.3 | 29 | 0.3
Hypocalcemia | 25 | 2.5 | 19 | 0.7
Hyperkalemia | 23 | 3.0 | 20 | 2.2
Increased prothrombin INR | 21 | 2.0 | 15 | 2.9
Hypophosphatemia | 20 | 4.7 | 17 | 4.3
Hematology
Anemia | 43 | 4.4 | 79 | 19
Lymphopenia | 30 | 7 | 42 | 13

Previously Treated NSCLC

The safety of intravenous pembrolizumab was investigated in KEYNOTE-010, a multicenter, open-label, randomized (1:1:1), active-controlled trial, in patients with advanced NSCLC who had documented disease progression following treatment with platinum-based chemotherapy and, if positive for EGFR or ALK genetic aberrations, appropriate therapy for these aberrations [see Clinical Studies (14.3)]. A total of 991 patients received intravenous pembrolizumab 2 mg/kg (n=339) or 10 mg/kg (n=343) every 3 weeks or docetaxel (n=309) at 75 mg/m^2 every 3 weeks. Patients with autoimmune disease, medical conditions that required systemic corticosteroids or other immunosuppressive medication, or who had received more than 30 Gy of thoracic radiation within the prior 26 weeks were ineligible.

The median duration of exposure to intravenous pembrolizumab 2 mg/kg every 3 weeks was 3.5 months (range: 1 day to 22.4 months) and to intravenous pembrolizumab 10 mg/kg every 3 weeks was 3.5 months (range 1 day to 20.8 months). The data described below reflect exposure to intravenous pembrolizumab 2 mg/kg in 31% of patients exposed to intravenous pembrolizumab for ≥6 months. In the intravenous pembrolizumab 10 mg/kg arm, 34% of patients were exposed to intravenous pembrolizumab for ≥6 months.

The study population characteristics were: median age of 63 years (range: 20 to 88), 42% age 65 or older; 61% male; 72% White and 21% Asian; and 8% with advanced localized disease, 91% with metastatic disease, and 15% with history of brain metastases. Twenty-nine percent received two or more prior systemic treatments for advanced or metastatic disease.

In KEYNOTE-010, the adverse reaction profile was similar for the 2 mg/kg and 10 mg/kg dose, therefore summary safety results are provided in a pooled analysis (n=682). Treatment was discontinued for adverse reactions in 8% of patients receiving intravenous pembrolizumab. The most common adverse events resulting in permanent discontinuation of intravenous pembrolizumab was pneumonitis (1.8%). Adverse reactions leading to interruption of intravenous pembrolizumab occurred in 23% of patients; the most common (≥1%) were diarrhea (1%), fatigue (1.3%), pneumonia (1%), liver enzyme elevation (1.2%), decreased appetite (1.3%), and pneumonitis (1%). Tables 16 and 17 summarize adverse reactions and laboratory abnormalities, respectively, in patients on intravenous pembrolizumab in KEYNOTE-010.

Table 16: Selected [Adverse reactions occurring at same or higher incidence than in docetaxel arm] Adverse Reactions Occurring in ≥10% of Patients Receiving Intravenous Pembrolizumab in KEYNOTE-010
Adverse Reaction | Intravenous Pembrolizumab 2 or 10 mg/kg every 3 weeks n=682 |  | Docetaxel 75 mg/m^2 every 3 weeks n=309
 | All Grades [Graded per NCI CTCAE v4.0] (%) | Grades 3-4 (%) | All Grades (%) | Grades 3-4 (%)
Metabolism and Nutrition
Decreased appetite | 25 | 1.5 | 23 | 2.6
Respiratory, Thoracic and Mediastinal
Dyspnea | 23 | 3.7 | 20 | 2.6
Cough | 19 | 0.6 | 14 | 0
Gastrointestinal
Nausea | 20 | 1.3 | 18 | 0.6
Constipation | 15 | 0.6 | 12 | 0.6
Vomiting | 13 | 0.9 | 10 | 0.6
Skin and Subcutaneous Tissue
Rash [Includes rash, rash erythematous, rash macular, rash maculo-papular, rash papular, and rash pruritic] | 17 | 0.4 | 8 | 0
Pruritus | 11 | 0 | 3 | 0.3
Musculoskeletal and Connective Tissue
Arthralgia | 11 | 1.0 | 9 | 0.3
Back pain | 11 | 1.5 | 8 | 0.3

Other clinically important adverse reactions occurring in patients receiving intravenous pembrolizumab were fatigue (25%), diarrhea (14%), asthenia (11%) and pyrexia (11%).

Table 17: Selected [Laboratory abnormalities occurring at same or higher incidence than in docetaxel arm.] Laboratory Abnormalities Worsened from Baseline Occurring in ≥20% of NSCLC Patients Receiving Intravenous Pembrolizumab in KEYNOTE-010
Laboratory Test [Each test incidence is based on the number of patients who had both baseline and at least one on-study laboratory measurement available: intravenous pembrolizumab (range: 631 to 638 patients) and docetaxel (range: 271 to 277 patients).] | Intravenous Pembrolizumab 2 or 10 mg/kg every 3 weeks |  | Docetaxel 75 mg/m^2 every 3 weeks
 | All Grades [Graded per NCI CTCAE v4.0] % | Grades 3-4 % | All Grades % | Grades 3-4 %
Chemistry
Hyponatremia | 32 | 8 | 27 | 2.9
Increased alkaline phosphatase | 28 | 3.0 | 16 | 0.7
Increased AST | 26 | 1.6 | 12 | 0.7
Increased ALT | 22 | 2.7 | 9 | 0.4
Hypocalcemia | 20 | 0.9 | 20 | 1.8

Other laboratory abnormalities occurring in ≥20% of patients receiving intravenous pembrolizumab were hyperglycemia (44% all Grades; 4.1% Grades 3-4), anemia (37% all Grades; 3.8% Grades 3-4), hypertriglyceridemia (36% all Grades; 1.8% Grades 3-4), lymphopenia (32% all Grades; 9% Grades 3-4), hypoalbuminemia (34% all Grades; 1.6% Grades 3-4), and hypercholesterolemia (20% all Grades; 0.7% Grades 3-4).

Neoadjuvant and Adjuvant Treatment of Resectable NSCLC

The safety of intravenous pembrolizumab in combination with neoadjuvant platinum-containing chemotherapy followed by surgery and continued adjuvant treatment with intravenous pembrolizumab as a single agent after surgery was investigated in KEYNOTE-671, a multicenter, randomized (1:1), double-blind, placebo-controlled trial in patients with previously untreated and resectable Stage II, IIIA, or IIIB (N2) NSCLC by AJCC 8th edition [see Clinical Studies (14.3)]. Patients with active autoimmune disease that required systemic therapy within 2 years of treatment or a medical condition that required immunosuppression were ineligible.

The median duration of exposure to intravenous pembrolizumab 200 mg every 3 weeks was 10.9 months (range: 1 day to 18.6 months). The study population characteristics were: median age of 64 years (range: 26 to 83), 45% age 65 or older, 7% age 75 or older; 71% male; 61% White, 31% Asian, 2% Black, 4% race not reported; 9% Hispanic or Latino.

Adverse reactions occurring in patients with resectable NSCLC receiving intravenous pembrolizumab in combination with platinum containing chemotherapy, given as neoadjuvant treatment and continued as single agent adjuvant treatment, were generally similar to those occurring in patients in other clinical trials across tumor types receiving intravenous pembrolizumab in combination with chemotherapy.

Neoadjuvant Phase of KEYNOTE-671

A total of 396 patients received at least 1 dose of intravenous pembrolizumab in combination with platinum-containing chemotherapy as neoadjuvant treatment and 399 patients received at least 1 dose of placebo in combination with platinum-containing chemotherapy as neoadjuvant treatment.

Serious adverse reactions occurred in 34% of patients who received intravenous pembrolizumab in combination with platinum-containing chemotherapy as neoadjuvant treatment; the most frequent (≥2%) serious adverse reactions were pneumonia (4.8%), venous thromboembolism (3.3%), and anemia (2%). Fatal adverse reactions occurred in 1.3% of patients, including death due to unknown cause (0.8%), sepsis (0.3%), and immune-mediated lung disease (0.3%).

Permanent discontinuation of any study drug due to an adverse reaction occurred in 18% of patients who received intravenous pembrolizumab in combination with platinum-containing chemotherapy as neoadjuvant treatment; the most frequent (≥1%) adverse reactions that led to permanent discontinuation of any study drug were acute kidney injury (1.8%), interstitial lung disease (1.8%), anemia (1.5%), neutropenia (1.5%), and pneumonia (1.3%).

Of the 396 intravenous pembrolizumab-treated patients and 399 placebo-treated patients who received neoadjuvant treatment, 6% (n=25) and 4.3% (n=17), respectively, did not receive surgery due to adverse reactions. The most frequent (≥1%) adverse reactions that led to cancellation of surgery in the intravenous pembrolizumab arm was interstitial lung disease (1%).

Of the 325 intravenous pembrolizumab-treated patients who received surgery, 3.1% (n=10) experienced delay of surgery (surgery more than 8 weeks from last neoadjuvant treatment if patient received less than 4 cycles of neoadjuvant therapy or more than 20 weeks after first dose of neoadjuvant treatment if patient received 4 cycles of neoadjuvant therapy) due to adverse reactions. Of the 317 placebo-treated patients who received surgery, 2.5% (n=8) experienced delay of surgery due to adverse reactions.

Of the 325 intravenous pembrolizumab-treated patients who received surgery, 7% (n=22) did not receive adjuvant treatment due to adverse reactions. Of the 317 placebo-treated patients who received surgery, 3.2% (n=10) did not receive adjuvant treatment due to adverse reactions.

Adjuvant Phase of KEYNOTE-671

A total of 290 patients in the intravenous pembrolizumab arm and 267 patients in the placebo arm received at least 1 dose of adjuvant treatment.

Of the patients who received single agent intravenous pembrolizumab as adjuvant treatment, 14% experienced serious adverse reactions; the most frequent serious adverse reaction was pneumonia (3.4%). One fatal adverse reaction of pulmonary hemorrhage occurred. Permanent discontinuation of adjuvant intravenous pembrolizumab due to an adverse reaction occurred in 12% of patients; the most frequent (≥1%) adverse reactions that led to permanent discontinuation of adjuvant intravenous pembrolizumab were diarrhea (1.7%), interstitial lung disease (1.4%), AST increased (1%), and musculoskeletal pain (1%).

Adjuvant Treatment of Resected NSCLC

The safety of intravenous pembrolizumab as a single agent was investigated in KEYNOTE-091, a multicenter, randomized (1:1), triple-blind, placebo-controlled trial in patients with completely resected Stage IB (T2a ≥4 cm), II, or IIIA NSCLC; adjuvant chemotherapy up to 4 cycles was optional [see Clinical Studies (14.3)]. A total of 1161 patients received intravenous pembrolizumab 200 mg (n=580) or placebo (n=581) every 3 weeks. Patients were ineligible if they had active autoimmune disease, were on chronic immunosuppressive agents, or had a history of interstitial lung disease or pneumonitis.

The median duration of exposure to intravenous pembrolizumab was 11.7 months (range: 1 day to 18.9 months). Sixty-eight percent of patients in the intravenous pembrolizumab arm were exposed to intravenous pembrolizumab for ≥6 months.

The adverse reactions observed in KEYNOTE-091 were generally similar to those occurring in other patients with NSCLC receiving intravenous pembrolizumab as a single agent, with the exception of hypothyroidism (22%), hyperthyroidism (11%), and pneumonitis (7%). Two fatal adverse reactions of myocarditis occurred.

Malignant Pleural Mesothelioma (MPM)

First-line treatment of unresectable advanced or metastatic MPM with pemetrexed and platinum chemotherapy

The safety of intravenous pembrolizumab in combination with pemetrexed and platinum chemotherapy (either carboplatin or cisplatin) was investigated in KEYNOTE-483, a multicenter, open-label, randomized (1:1), active-controlled trial in patients with previously untreated, unresectable advanced or metastatic MPM [see Clinical Studies (14.4)]. A total of 473 patients received intravenous pembrolizumab 200 mg, pemetrexed, and platinum every 3 weeks for up to 6 cycles followed by intravenous pembrolizumab (n=241), or pemetrexed and platinum chemotherapy every 3 weeks for up to 6 cycles (n=232). Patients with autoimmune disease that required systemic therapy within 3 years of treatment or a medical condition that required immunosuppression were ineligible.

The median duration of exposure to intravenous pembrolizumab 200 mg every 3 weeks was 6.9 months (range: 1 day to 25.2 months). Sixty-one percent of patients in the intravenous pembrolizumab arm were exposed to intravenous pembrolizumab for ≥6 months.

Adverse reactions occurring in patients with MPM were generally similar to those in other patients receiving intravenous pembrolizumab in combination with pemetrexed and platinum chemotherapy.

HNSCC

Neoadjuvant and Adjuvant Treatment of Locally Advanced HNSCC

The safety of intravenous pembrolizumab as neoadjuvant and adjuvant treatment added to standard of care (SOC) therapy was evaluated in KEYNOTE-689, a multicenter, randomized (1:1), open-label, active-controlled trial in patients with resectable locally advanced (Stage III-IVA by AJCC 8th edition) head and neck squamous cell carcinoma (HNSCC) [see Clinical Studies (14.5)]. Intravenous pembrolizumab was administered as single-agent neoadjuvant therapy before definitive surgery, during adjuvant radiotherapy (RT) with or without concurrent cisplatin, and then as single agent adjuvant therapy. Concurrent cisplatin was added to intravenous pembrolizumab and adjuvant RT for high-risk disease pathology. A total of 361 patients received treatment on the intravenous pembrolizumab arm and 315 patients received treatment on the SOC therapy arm.

The median duration of exposure to intravenous pembrolizumab in the neoadjuvant phase was 3.1 weeks (range: 1 day to 4.9 weeks). The median duration of exposure to intravenous pembrolizumab in the adjuvant phase was 42 weeks (range: 1 day to 82 weeks).

The median age of patients who received intravenous pembrolizumab was 60 years (range: 29 to 82), 32% age 65 or older, 6% age 75 or older; 79% male; 78% White, 14% Asian, 2.2% Black or African American, 2% Other races, 2.7% unknown race; and 15% Hispanic or Latino.

The most common adverse reactions (≥ 20%) on the intravenous pembrolizumab arm were stomatitis (48%), radiation skin injury (40%), weight loss (36%), fatigue (33%), dysphagia (29%), constipation (27%), hypothyroidism (26%), nausea (24%), rash (22%), dry mouth (22%), diarrhea (22%), and musculoskeletal pain (22%).

Table 18 and Table 19 summarize adverse reactions and laboratory abnormalities, respectively, in patients on intravenous pembrolizumab in KEYNOTE-689.

Table 18: Adverse Reactions in ≥20% of Patients with HNSCC Who Received Intravenous Pembrolizumab in KEYNOTE-689
Adverse Reaction | Intravenous Pembrolizumab Neoadjuvant then adjuvant beginning with RT with or without cisplatin n=361 |  | Standard of Care Adjuvant RT with or without cisplatin n=315
 | All Grades [Graded per NCI CTCAE v4.03] (%) | Grade 3 or 4 (%) | All Grades (%) | Grade 3 or 4 (%)
Gastrointestinal
Stomatitis [Includes pharyngeal inflammation, cheilitis, oral mucosal erythema, mucosal inflammation, glossitis, mouth ulceration, tongue ulceration] | 48 | 14 | 60 | 13
Dysphagia | 29 | 12 | 32 | 11
Constipation | 27 | 0.3 | 22 | 0.3
Nausea | 24 | 1.9 | 28 | 2.9
Dry mouth | 22 | 1.4 | 26 | 1.6
Diarrhea [Includes colitis, enteritis, hemorrhagic diarrhea] | 22 | 4.2 | 11 | 0.6
Injury, poisoning and procedural complications
Radiation skin injury | 40 | 4.2 | 48 | 5.7
Investigations
Weight loss | 36 | 14 | 27 | 10
Endocrine disorders
Hypothyroidism [Includes blood thyroid stimulating hormone increased] | 26 | 0 | 6 | 0
General
Fatigue [Includes asthenia] | 33 | 2.2 | 27 | 1.6
Skin and subcutaneous tissue disorders
Rash [Includes dermatitis, skin exfoliation, dermatitis acneiform, eczema, rash macular, rash maculo-papular, erythema multiforme, dermatitis exfoliative, urticarial dermatitis, eczema asteatotic, exfoliative rash, rash pruritic, rash pustular] | 22 | 1.9 | 10 | 1.9
Musculoskeletal and connective tissue disorders
Musculoskeletal pain [Includes neck pain, arthralgia, pain in extremity, back pain, myalgia, bone pain, arthritis, non-cardiac chest pain, musculoskeletal chest pain, musculoskeletal stiffness, spinal pain] | 22 | 1.9 | 16 | 0.6

Table 19: Select Laboratory Abnormalities (≥20%) that Worsened from Baseline in Patients with HNSCC Who Received Intravenous Pembrolizumab in KEYNOTE-689
Laboratory Test [Each test incidence is based on the number of patients who had both baseline and at least one on-study laboratory measurement available: Intravenous Pembrolizumab + CRT/RT (range: 342 to 357 patients) and CRT/RT (range: 300 to 309 patients)] | Intravenous Pembrolizumab Neoadjuvant then adjuvant beginning with radiation with or without cisplatin |  | Radiation with or without cisplatin
Laboratory Test [Each test incidence is based on the number of patients who had both baseline and at least one on-study laboratory measurement available: Intravenous Pembrolizumab + CRT/RT (range: 342 to 357 patients) and CRT/RT (range: 300 to 309 patients)] | All Grades [Graded per NCI CTCAE v4.03] (%) | Grades 3-4 (%) | All Grades (%) | Grades 3-4 (%)
Hematology
Lymphopenia | 76 | 50 | 86 | 55
Anemia | 75 | 12 | 74 | 12
Neutropenia | 32 | 13 | 35 | 19
Thrombocytopenia | 22 | 1.7 | 29 | 1.9
Chemistry
Hyperglycemia | 57 | 5.7 | 47 | 2.7
Hyponatremia | 47 | 16 | 36 | 11
Increased ALT | 42 | 6.2 | 37 | 2.0
Hypoalbuminemia | 40 | 1.4 | 38 | 1.0
Increased AST | 38 | 4.8 | 23 | 2.0
Hypomagnesemia | 34 | 1.2 | 22 | 1.3
Hypokalemia | 29 | 6.8 | 20 | 7.4
Hyperkalemia | 29 | 3.4 | 24 | 2.3
Increased alkaline phosphatase | 27 | 2.5 | 19 | 0.0
Hypocalcemia | 27 | 2.6 | 26 | 3.3
Hypophosphatemia | 23 | 6.1 | 15 | 7.0
Increased creatinine | 22 | 2.0 | 27 | 2.9
Hypercalcemia | 21 | 2.0 | 14 | 1.3

Neoadjuvant Phase of KEYNOTE-689

Of the 361 patients who received at least one dose of single agent intravenous pembrolizumab as neoadjuvant treatment, 11% of patients experienced serious adverse reactions. Serious adverse reactions that occurred in more than one patient were pneumonia (1.4%), tumor hemorrhage (0.8%), dysphagia (0.6%), immune mediated hepatitis (0.6%), cellulitis (0.6%), and dyspnea (0.6%). Fatal adverse reactions occurred in 1.1% of patients who received neoadjuvant intravenous pembrolizumab including respiratory failure, clostridium infection, septic shock, and myocardial infarction (one patient each).

Permanent discontinuation of intravenous pembrolizumab due to an adverse reaction occurred in 2.8% of patients who received intravenous pembrolizumab as neoadjuvant treatment. The most frequent adverse reaction which resulted in permanent discontinuation of neoadjuvant intravenous pembrolizumab in more than one patient was arthralgia (0.6%).

Of the 361 patients who received intravenous pembrolizumab as neoadjuvant treatment, 11% (n=38) did not receive surgery. Surgical cancellation on the intravenous pembrolizumab arm was due to disease progression in 4% (n=15), patient decision in 3% (n=10), adverse reactions in 1.4% (n=5), physician’s decision in 1.1% (n=4), unresectable tumor in 0.6% (n=2), loss of follow-up in 0.3% (n=1), and use of non-study anti-cancer therapy in 0.3% (n=1).

Of the 351 patients randomized to SOC, 12% (n=43) did not receive surgery. Surgical cancellation on the SOC arm was due to patient decision in 7% (n=24), physician’s decision in 2.3% (n=8), disease progression in 1.7% (n=6), and adverse reactions in 1.4% (n=5).

Of the 323 intravenous pembrolizumab-treated patients who received surgery, 1.2% (n=4) experienced delay of surgery (defined as on-study surgery occurring ≥ 9 weeks after initiation of neoadjuvant intravenous pembrolizumab) due to adverse reactions. Of the 307 patients randomized to SOC who received surgery on study, 0.3% (n=1) experienced delay of surgery (defined as surgery occurring ≥ 6 weeks after randomization) due to adverse reactions.

Among the intravenous pembrolizumab-treated patients who received surgery, 2.8% (n=9) did not receive adjuvant treatment due to adverse reactions. Among the SOC-treated patients who received surgery, 3.6% (n=11) did not receive adjuvant RT or chemoradiation due to adverse reactions.

Adjuvant Phase of KEYNOTE-689

A total of 275 patients in the intravenous pembrolizumab arm and 275 patients in the SOC arm started the adjuvant phase of treatment. On the intravenous pembrolizumab arm, 100 patients received intravenous pembrolizumab and cisplatin with concurrent RT, 154 patients received intravenous pembrolizumab alone with concurrent RT, 7 patients received cisplatin alone with concurrent RT, and 13 patients received RT alone. One patient received intravenous pembrolizumab alone. On the SOC arm, 139 patients received cisplatin with concurrent RT while 136 patients received RT alone. For the intravenous pembrolizumab arm, a total of 222 patients received single-agent intravenous pembrolizumab following RT.

Of the 255 patients who received at least one dose of intravenous pembrolizumab in the adjuvant phase, 38% experienced serious adverse reactions. The most frequent serious adverse reactions reported in ≥1% of intravenous pembrolizumab-treated patients were pneumonia (2.7%), pyrexia (2.4%), stomatitis (2.4%), acute kidney injury (2.0%), pneumonitis (1.6%), COVID-19 (1.2%), death not otherwise specified (1.2%), diarrhea (1.2%), dysphagia (1.2%), gastrostomy tube site complication (1.2%), and immune-mediated hepatitis (1.2%).

Fatal adverse reactions occurred in 5% including death not otherwise specified (1.2%), acute renal failure (0.4%), hypercalcemia (0.4%), pulmonary hemorrhage (0.4%), dysphagia/malnutrition (0.4%), mesenteric thrombosis (0.4%), sepsis (0.4%), pneumonia (0.4%), COVID-19 (0.4%), respiratory failure (0.4%), cardiovascular disorder (0.4%) and gastrointestinal hemorrhage (0.4%).

Permanent discontinuation of adjuvant intravenous pembrolizumab due to an adverse reaction occurred in 17% of patients. The most frequent (≥1%) adverse reactions that led to permanent discontinuation of adjuvant intravenous pembrolizumab were pneumonitis, colitis, immune-mediated hepatitis and death not otherwise specified.

Of the 275 patients who received SOC in the adjuvant phase, 23% experienced serious adverse reactions.

The most frequent serious adverse reactions reported in >1% of SOC-treated patients were pneumonia (3.6%) and acute kidney injury (3.3%). Fatal adverse reactions occurred in 4.7% including pneumonia (0.7%), septic shock (0.4%), death not otherwise specified (0.4%), sudden death (0.4%), myocardial infarction (0.4%), pancreatic neoplasm (0.4%) and other infections (2.9%).

First-line treatment of metastatic or unresectable, recurrent HNSCC

The safety of intravenous pembrolizumab, as a single agent and in combination with platinum (cisplatin or carboplatin) and FU chemotherapy, was investigated in KEYNOTE-048, a multicenter, open-label, randomized (1:1:1), active-controlled trial in patients with previously untreated, recurrent or metastatic HNSCC [see Clinical Studies (14.5)]. Patients with autoimmune disease that required systemic therapy within 2 years of treatment or a medical condition that required immunosuppression were ineligible. A total of 576 patients received intravenous pembrolizumab 200 mg every 3 weeks either as a single agent (n=300) or in combination with platinum and FU (n=276) every 3 weeks for 6 cycles followed by intravenous pembrolizumab, compared to 287 patients who received cetuximab weekly in combination with platinum and FU every 3 weeks for 6 cycles followed by cetuximab.

The median duration of exposure to intravenous pembrolizumab was 3.5 months (range: 1 day to 24.2 months) in the intravenous pembrolizumab single agent arm and was 5.8 months (range: 3 days to 24.2 months) in the combination arm. Seventeen percent of patients in the intravenous pembrolizumab single agent arm and 18% of patients in the combination arm were exposed to intravenous pembrolizumab for ≥12 months. Fifty-seven percent of patients receiving intravenous pembrolizumab in combination with chemotherapy started treatment with carboplatin.

Intravenous pembrolizumab was discontinued for adverse reactions in 12% of patients in the intravenous pembrolizumab single agent arm. The most common adverse reactions resulting in permanent discontinuation of intravenous pembrolizumab were sepsis (1.7%) and pneumonia (1.3%). Adverse reactions leading to the interruption of intravenous pembrolizumab occurred in 31% of patients; the most common adverse reactions leading to interruption of intravenous pembrolizumab (≥2%) were pneumonia (2.3%), pneumonitis (2.3%), and hyponatremia (2%).

Intravenous pembrolizumab was discontinued for adverse reactions in 16% of patients in the combination arm. The most common adverse reactions resulting in permanent discontinuation of intravenous pembrolizumab were pneumonia (2.5%), pneumonitis (1.8%), and septic shock (1.4%). Adverse reactions leading to the interruption of intravenous pembrolizumab occurred in 45% of patients; the most common adverse reactions leading to interruption of intravenous pembrolizumab (≥2%) were neutropenia (14%), thrombocytopenia (10%), anemia (6%), pneumonia (4.7%), and febrile neutropenia (2.9%).

Tables 20 and 21 summarize adverse reactions and laboratory abnormalities, respectively, in patients on intravenous pembrolizumab in KEYNOTE-048.

Table 20: Adverse Reactions Occurring in ≥10% of Patients Receiving Intravenous Pembrolizumab in KEYNOTE-048
 | Intravenous Pembrolizumab 200 mg every 3 weeks |  | Intravenous Pembrolizumab 200 mg every 3 weeks Platinum FU |  | Cetuximab Platinum FU
Adverse Reaction | n=300 |  | n=276 |  | n=287
 | All Grades [Graded per NCI CTCAE v4.0] (%) | Grades 3-4 (%) | All Grades (%) | Grades 3-4 (%) | All Grades (%) | Grades 3-4 (%)
General
Fatigue [Includes fatigue, asthenia] | 33 | 4 | 49 | 11 | 48 | 8
Pyrexia | 13 | 0.7 | 16 | 0.7 | 12 | 0
Mucosal inflammation | 4.3 | 1.3 | 31 | 10 | 28 | 5
Gastrointestinal
Constipation | 20 | 0.3 | 37 | 0 | 33 | 1.4
Nausea | 17 | 0 | 51 | 6 | 51 | 6
Diarrhea [Includes diarrhea, colitis, hemorrhagic diarrhea, microscopic colitis] | 16 | 0.7 | 29 | 3.3 | 35 | 3.1
Vomiting | 11 | 0.3 | 32 | 3.6 | 28 | 2.8
Dysphagia | 8 | 2.3 | 12 | 2.9 | 10 | 2.1
Stomatitis | 3 | 0 | 26 | 8 | 28 | 3.5
Skin
Rash [Includes dermatitis, dermatitis acneiform, dermatitis allergic, dermatitis bullous, dermatitis contact, dermatitis exfoliative, drug eruption, erythema, erythema multiforme, rash, erythematous rash, generalized rash, macular rash, maculo-papular rash, pruritic rash, seborrheic dermatitis] | 20 | 2.3 | 17 | 0.7 | 70 | 8
Pruritus | 11 | 0 | 8 | 0 | 10 | 0.3
Respiratory, Thoracic and Mediastinal
Cough [Includes cough, productive cough] | 18 | 0.3 | 22 | 0 | 15 | 0
Dyspnea [Includes dyspnea, exertional dyspnea] | 14 | 2.0 | 10 | 1.8 | 8 | 1.0
Endocrine
Hypothyroidism | 18 | 0 | 15 | 0 | 6 | 0
Metabolism and Nutrition
Decreased appetite | 15 | 1.0 | 29 | 4.7 | 30 | 3.5
Weight loss | 15 | 2 | 16 | 2.9 | 21 | 1.4
Infections
Pneumonia [Includes pneumonia, atypical pneumonia, bacterial pneumonia, staphylococcal pneumonia, aspiration pneumonia, lower respiratory tract infection, lung infection, lung infection pseudomonal] | 12 | 7 | 19 | 11 | 13 | 6
Nervous System
Headache | 12 | 0.3 | 11 | 0.7 | 8 | 0.3
Dizziness | 5 | 0.3 | 10 | 0.4 | 13 | 0.3
Peripheral sensory neuropathy [Includes peripheral sensory neuropathy, peripheral neuropathy, hypoesthesia, dysesthesia] | 1 | 0 | 14 | 1.1 | 7 | 1
Musculoskeletal
Myalgia [Includes back pain, musculoskeletal chest pain, musculoskeletal pain, myalgia] | 12 | 1.0 | 13 | 0.4 | 11 | 0.3
Neck pain | 6 | 0.7 | 10 | 1.1 | 7 | 0.7
Psychiatric
Insomnia | 7 | 0.7 | 10 | 0 | 8 | 0

Table 21: Laboratory Abnormalities Worsened from Baseline Occurring in ≥20% of Patients Receiving Intravenous Pembrolizumab in KEYNOTE-048
Laboratory Test [Each test incidence is based on the number of patients who had both baseline and at least one on-study laboratory measurement available: intravenous pembrolizumab/chemotherapy (range: 240 to 267 patients), intravenous pembrolizumab (range: 245 to 292 patients), cetuximab/chemotherapy (range: 249 to 282 patients).] | Intravenous Pembrolizumab 200 mg every 3 weeks |  | Intravenous Pembrolizumab 200 mg every 3 weeks Platinum FU |  | Cetuximab Platinum FU
Laboratory Test [Each test incidence is based on the number of patients who had both baseline and at least one on-study laboratory measurement available: intravenous pembrolizumab/chemotherapy (range: 240 to 267 patients), intravenous pembrolizumab (range: 245 to 292 patients), cetuximab/chemotherapy (range: 249 to 282 patients).] | All Grades [Graded per NCI CTCAE v4.0] (%) | Grades 3-4 (%) | All Grades (%) | Grades 3-4 (%) | All Grades (%) | Grades 3-4 (%)
Hematology
Lymphopenia | 54 | 25 | 70 | 35 | 75 | 46
Anemia | 52 | 7 | 89 | 29 | 79 | 20
Thrombocytopenia | 12 | 3.8 | 73 | 18 | 76 | 18
Neutropenia | 8 | 1.4 | 68 | 37 | 73 | 43
Chemistry
Hyperglycemia | 47 | 3.8 | 54 | 6 | 65 | 4.7
Hyponatremia | 46 | 18 | 55 | 20 | 59 | 20
Hypoalbuminemia | 44 | 3.5 | 46 | 3.9 | 49 | 1.1
Increased AST | 28 | 3.1 | 25 | 1.9 | 37 | 3.6
Increased ALT | 25 | 2.1 | 22 | 1.5 | 38 | 1.8
Increased alkaline phosphatase | 25 | 2.1 | 26 | 1.1 | 33 | 1.1
Hypercalcemia | 22 | 4.5 | 16 | 4.2 | 13 | 2.5
Hypocalcemia | 22 | 1.0 | 32 | 3.8 | 58 | 6
Hyperkalemia | 21 | 2.8 | 28 | 4.2 | 29 | 4.6
Hypophosphatemia | 20 | 5 | 34 | 12 | 49 | 20
Hypokalemia | 19 | 5 | 33 | 12 | 47 | 15
Increased creatinine | 17 | 1.0 | 36 | 2.3 | 27 | 2.1
Hypomagnesemia | 15 | 0.4 | 40 | 1.7 | 76 | 9

Previously treated recurrent or metastatic HNSCC

Among the 192 patients with HNSCC enrolled in KEYNOTE-012 [see Clinical Studies (14.5)], the median duration of exposure to intravenous pembrolizumab was 3.3 months (range: 1 day to 27.9 months). Patients with autoimmune disease or a medical condition that required immunosuppression were ineligible for KEYNOTE-012.

The study population characteristics were: median age of 60 years (range: 20 to 84), 35% age 65 or older; 83% male; and 77% White, 15% Asian, and 5% Black. Sixty-one percent of patients had two or more lines of therapy in the recurrent or metastatic setting, and 95% had prior radiation therapy. Baseline ECOG PS was 0 (30%) or 1 (70%) and 86% had M1 disease.

Intravenous pembrolizumab was discontinued due to adverse reactions in 17% of patients. Serious adverse reactions occurred in 45% of patients receiving intravenous pembrolizumab. The most frequent serious adverse reactions reported in at least 2% of patients were pneumonia, dyspnea, confusional state, vomiting, pleural effusion, and respiratory failure. The incidence of adverse reactions, including serious adverse reactions, was similar between dosage regimens (10 mg/kg every 2 weeks or 200 mg every 3 weeks); therefore, summary safety results are provided in a pooled analysis. The most common adverse reactions (occurring in ≥20% of patients) were fatigue, decreased appetite, and dyspnea. Adverse reactions occurring in patients with HNSCC were generally similar to those occurring in 2799 patients with melanoma or NSCLC treated with intravenous pembrolizumab as a single agent, with the exception of increased incidences of facial edema (10% all Grades; 2.1% Grades 3-4) and new or worsening hypothyroidism [see Warnings and Precautions (5.1)].

Urothelial Cancer

Patients with urothelial cancer in combination with enfortumab vedotin

The safety of intravenous pembrolizumab in combination with enfortumab vedotin was investigated in KEYNOTE-A39 in patients with locally advanced or metastatic urothelial cancer [see Clinical Studies (14.6)]. A total of 440 patients received intravenous pembrolizumab 200 mg on Day 1 and enfortumab vedotin 1.25 mg/kg on Days 1 and 8 of each 21-day cycle compared to 433 patients who received gemcitabine on Days 1 and 8 and investigator’s choice of cisplatin or carboplatin on Day 1 of each 21-day cycle. Among patients who received intravenous pembrolizumab and enfortumab vedotin, the median duration of exposure to intravenous pembrolizumab was 8.5 months (range: 9 days to 28.5 months).

Fatal adverse reactions occurred in 3.9% of patients treated with intravenous pembrolizumab in combination with enfortumab vedotin including acute respiratory failure (0.7%), pneumonia (0.5%), and pneumonitis/ILD (0.2%).

Serious adverse reactions occurred in 50% of patients receiving intravenous pembrolizumab in combination with enfortumab vedotin. Serious adverse reactions in ≥2% of patients receiving intravenous pembrolizumab in combination with enfortumab vedotin were rash (6%), acute kidney injury (5%), pneumonitis/ILD (4.5%), urinary tract infection (3.6%), diarrhea (3.2%), pneumonia (2.3%), pyrexia (2%), and hyperglycemia (2%).

Permanent discontinuation of intravenous pembrolizumab occurred in 27% of patients. The most common adverse reactions (≥2%) resulting in permanent discontinuation of intravenous pembrolizumab were pneumonitis/ILD (4.8%) and rash (3.4%).

Dose interruptions of intravenous pembrolizumab occurred in 61% of patients. The most common adverse reactions (≥2%) resulting in interruption of intravenous pembrolizumab were rash (17%), peripheral neuropathy (7%), COVID-19 (5%), diarrhea (4.3%), pneumonitis/ILD (3.6%), neutropenia (3.4%), fatigue (3%), alanine aminotransferase increased (2.7%), hyperglycemia (2.5%), pneumonia (2%), and pruritus (2%).

Tables 22 and 23 summarize adverse reactions and laboratory abnormalities, respectively, in patients on intravenous pembrolizumab in combination with enfortumab vedotin in KEYNOTE-A39.

Table 22: Adverse Reactions ≥20% (All Grades) in Patients Treated with Intravenous Pembrolizumab in Combination with Enfortumab Vedotin in KEYNOTE-A39
Adverse Reaction | Intravenous Pembrolizumab in combination with Enfortumab Vedotin n=440 |  | Chemotherapy n=433
Adverse Reaction | All Grades [Graded per NCI CTCAE v4.03] % | Grades 3-4 % | All Grades % | Grades 3-4 %
Skin and subcutaneous tissue disorders
Rash [Includes multiple terms] | 68 | 15 | 15 | 0
Pruritus | 41 | 1.1 | 7 | 0
Alopecia | 35 | 0.5 | 8 | 0.2
General disorders and administration site conditions
Fatigue | 51 | 6 | 57 | 7
Nervous system disorders
Peripheral neuropathy | 67 | 8 | 14 | 0
Dysgeusia | 21 | 0 | 9 | 0
Metabolism and nutrition disorders
Decreased appetite | 33 | 1.8 | 26 | 1.8
Gastrointestinal disorders
Diarrhea | 38 | 4.5 | 16 | 1.4
Nausea | 26 | 1.6 | 41 | 2.8
Constipation | 26 | 0 | 34 | 0.7
Investigations
Weight loss | 33 | 3.6 | 9 | 0.2
Eye disorders
Dry eye | 24 | 0 | 2.1 | 0
Infections and infestations
Urinary tract infection | 21 | 5 | 19 | 8

Clinically relevant adverse reactions (<20%) include pyrexia (18%), dry skin (17%), vomiting (12%), pneumonitis/ILD (10%), hypothyroidism (10%), blurred vision (6%), infusion site extravasation (2%), and myositis (0.5%).

Table 23: Selected Laboratory Abnormalities Worsened from Baseline Occurring in ≥20% of Patients in KEYNOTE-A39
Laboratory Test [Each test incidence is based on the number of patients who had both baseline and at least one on-study laboratory measurement available: intravenous pembrolizumab (range: 407 to 439 patients)] | Intravenous Pembrolizumab 200 mg every 3 weeks and Enfortumab Vedotin |  | Chemotherapy
Laboratory Test [Each test incidence is based on the number of patients who had both baseline and at least one on-study laboratory measurement available: intravenous pembrolizumab (range: 407 to 439 patients)] | All Grades [Graded per NCI CTCAE v4.03] % | Grades 3-4 % | All Grades % | Grades 3-4 %
Chemistry
Increased aspartate aminotransferase | 75 | 4.6 | 39 | 3.3
Increased creatinine | 71 | 3.2 | 68 | 2.6
Hyperglycemia | 66 | 14 | 54 | 4.7
Increased alanine aminotransferase | 59 | 5 | 49 | 3.3
Hyponatremia | 46 | 13 | 47 | 13
Hypophosphatemia | 44 | 9 | 36 | 9
Hypoalbuminemia | 39 | 1.8 | 35 | 0.5
Hypokalemia | 26 | 5 | 16 | 3.1
Hyperkalemia | 24 | 1.4 | 36 | 4.0
Hypercalcemia | 21 | 1.2 | 14 | 0.2
Hematology
Lymphopenia | 58 | 15 | 59 | 17
Anemia | 53 | 7 | 89 | 33
Neutropenia | 30 | 9 | 80 | 50

Cisplatin-ineligible patients with urothelial cancer in combination with enfortumab vedotin

The safety of intravenous pembrolizumab in combination with enfortumab vedotin was investigated in KEYNOTE-869 in patients with locally advanced or metastatic urothelial cancer and who are not eligible for cisplatin-based chemotherapy [see Clinical Studies (14.6)]. A total of 121 patients received intravenous pembrolizumab 200 mg on Day 1, and enfortumab vedotin 1.25 mg/kg on days 1 and 8 of each 21-day cycle. The median duration of exposure to intravenous pembrolizumab was 6.9 months (range 1 day to 29.6 months).

Fatal adverse reactions occurred in 5% of patients treated with intravenous pembrolizumab in combination with enfortumab vedotin, including sepsis (1.6%), bullous dermatitis (0.8%), myasthenia gravis (0.8%), and pneumonitis (0.8%).

Serious adverse reactions occurred in 50% of patients receiving intravenous pembrolizumab and enfortumab vedotin. Serious adverse reactions in ≥2% of patients receiving intravenous pembrolizumab in combination with enfortumab vedotin were acute kidney injury (7%), urinary tract infection (7%), urosepsis (5%), hematuria (3.3%), pneumonia (3.3%), pneumonitis (3.3%), sepsis (3.3%), anemia (2.5%), diarrhea (2.5%), hypotension (2.5%), myasthenia gravis (2.5%), myositis (2.5%), and urinary retention (2.5%).

Permanent discontinuation of intravenous pembrolizumab occurred in 32% of patients. The most common adverse reactions (≥2%) resulting in permanent discontinuation of intravenous pembrolizumab were pneumonitis (5%), peripheral neuropathy (5%), rash (3.3%), and myasthenia gravis (2.5%).

Dose interruptions of intravenous pembrolizumab occurred in 69% of patients. The most common adverse reactions (≥2%) resulting in interruption of intravenous pembrolizumab were peripheral neuropathy (22%), rash (17%), neutropenia (7%), fatigue (6%), diarrhea (5%), lipase increased (5%), acute kidney injury (3.3%), ALT increased (2.5%), and COVID-19 (2.5%).

Tables 24 and 25 summarize adverse reactions and laboratory abnormalities, respectively, in patients on intravenous pembrolizumab in combination with enfortumab vedotin in KEYNOTE-869.

Table 24: Adverse Reactions Occurring in ≥20% of Patients Treated with Intravenous Pembrolizumab in Combination with Enfortumab Vedotin in KEYNOTE-869
Adverse Reaction | Intravenous Pembrolizumab in combination with Enfortumab Vedotin n=121
Adverse Reaction | All Grades [Graded per NCI CTCAE v4.03] % | Grade 3-4 %
Skin and subcutaneous tissue disorders
Rash [Includes: blister, conjunctivitis, dermatitis, dermatitis bullous, dermatitis exfoliative generalized, erythema, erythema multiforme, exfoliative rash, palmar-plantar erythrodysesthesia syndrome, pemphigoid, rash, rash erythematous, rash macular, rash maculo-papular, rash papular, rash pruritic, rash vesicular, skin exfoliation, and stomatitis] | 71 | 21
Alopecia | 52 | 0
Pruritus | 40 | 3.3
Dry skin | 21 | 0.8
Nervous system disorders
Peripheral neuropathy [Includes: dysesthesia, hypoesthesia, muscular weakness, paresthesia, peripheral motor neuropathy, peripheral sensorimotor neuropathy, peripheral sensory neuropathy, and gait disturbance] | 65 | 3.3
Dysgeusia | 35 | 0
Dizziness | 23 | 0
General disorders and administration site conditions
Fatigue | 60 | 11
Peripheral edema | 26 | 0
Investigations
Weight loss | 48 | 5
Gastrointestinal disorders
Diarrhea | 45 | 7
Nausea | 36 | 0.8
Constipation | 27 | 0
Metabolism and nutrition disorders
Decreased appetite | 38 | 0.8
Infections and infestations
Urinary tract infection | 30 | 12
Eye disorders
Dry eye | 25 | 0
Musculoskeletal and connective tissue disorders
Arthralgia | 23 | 1.7

Clinically relevant adverse reactions (<20%) include vomiting (19.8%), fever (18%), hypothyroidism (11%), pneumonitis/ILD (10%), myositis (3.3%), myasthenia gravis (2.5%), and infusion site extravasation (0.8%).

Table 25: Selected Laboratory Abnormalities Worsened from Baseline Occurring in ≥20% of Patients in KEYNOTE-869
Laboratory Test [Each test incidence is based on the number of patients who had both baseline and at least one on-study laboratory measurement available: intravenous pembrolizumab (range: 114 to 121 patients)] | Intravenous Pembrolizumab 200 mg every 3 weeks and Enfortumab Vedotin
Laboratory Test [Each test incidence is based on the number of patients who had both baseline and at least one on-study laboratory measurement available: intravenous pembrolizumab (range: 114 to 121 patients)] | All Grades [Graded per NCI CTCAE v4.03] % | Grades 3-4 %
Chemistry
Hyperglycemia | 74 | 13
Increased aspartate aminotransferase | 73 | 9
Increased creatinine | 69 | 3.3
Hyponatremia | 60 | 19
Increased alanine aminotransferase | 60 | 7
Increased lipase | 59 | 32
Hypoalbuminemia | 59 | 4.2
Hypophosphatemia | 51 | 15
Hypokalemia | 35 | 8
Increased potassium | 27 | 1.7
Increased calcium | 27 | 4.2
Hematology
Anemia | 69 | 15
Lymphopenia | 64 | 17
Neutropenia | 32 | 12

Platinum-Ineligible Patients with Urothelial Carcinoma

The safety of intravenous pembrolizumab was investigated in KEYNOTE-052, a single-arm trial that enrolled 370 patients with locally advanced or metastatic urothelial carcinoma who had one or more comorbidities. Patients with autoimmune disease or medical conditions that required systemic corticosteroids or other immunosuppressive medications were ineligible [see Clinical Studies (14.6)]. Patients received intravenous pembrolizumab 200 mg every 3 weeks until unacceptable toxicity or either radiographic or clinical disease progression.

The median duration of exposure to intravenous pembrolizumab was 2.8 months (range: 1 day to 15.8 months).

Intravenous pembrolizumab was discontinued due to adverse reactions in 11% of patients. Eighteen patients (5%) died from causes other than disease progression. Five patients (1.4%) who were treated with intravenous pembrolizumab experienced sepsis which led to death, and three patients (0.8%) experienced pneumonia which led to death. Adverse reactions leading to interruption of intravenous pembrolizumab occurred in 22% of patients; the most common (≥1%) were liver enzyme increase, diarrhea, urinary tract infection, acute kidney injury, fatigue, joint pain, and pneumonia. Serious adverse reactions occurred in 42% of patients. The most frequent serious adverse reactions (≥2%) were urinary tract infection, hematuria, acute kidney injury, pneumonia, and urosepsis.

Immune-related adverse reactions that required systemic glucocorticoids occurred in 8% of patients, use of hormonal supplementation due to an immune-related adverse reaction occurred in 8% of patients, and 5% of patients required at least one steroid dose ≥40 mg oral prednisone equivalent.

Table 26 summarizes adverse reactions in patients on intravenous pembrolizumab in KEYNOTE-052.

Table 26: Adverse Reactions Occurring in ≥10% of Patients Receiving Intravenous Pembrolizumab in KEYNOTE-052
Adverse Reaction | Intravenous Pembrolizumab 200 mg every 3 weeks N=370
 | All Grades [Graded per NCI CTCAE v4.0] (%) | Grades 3–4 (%)
General
Fatigue [Includes fatigue, asthenia] | 38 | 6
Pyrexia | 11 | 0.5
Weight loss | 10 | 0
Musculoskeletal and Connective Tissue
Musculoskeletal pain [Includes back pain, bone pain, musculoskeletal chest pain, musculoskeletal pain, myalgia, neck pain, pain in extremity, spinal pain] | 24 | 4.9
Arthralgia | 10 | 1.1
Metabolism and Nutrition
Decreased appetite | 22 | 1.6
Hyponatremia | 10 | 4.1
Gastrointestinal
Constipation | 21 | 1.1
Diarrhea [Includes diarrhea, colitis, enterocolitis, gastroenteritis, frequent bowel movements] | 20 | 2.4
Nausea | 18 | 1.1
Abdominal pain [Includes abdominal pain, pelvic pain, flank pain, abdominal pain lower, tumor pain, bladder pain, hepatic pain, suprapubic pain, abdominal discomfort, abdominal pain upper] | 18 | 2.7
Elevated LFTs [Includes autoimmune hepatitis, hepatitis, hepatitis toxic, liver injury, increased transaminases, hyperbilirubinemia, increased blood bilirubin, increased alanine aminotransferase, increased aspartate aminotransferase, increased hepatic enzymes, increased liver function tests] | 13 | 3.5
Vomiting | 12 | 0
Skin and Subcutaneous Tissue
Rash [Includes dermatitis, dermatitis bullous, eczema, erythema, rash, rash macular, rash maculo-papular, rash pruritic, rash pustular, skin reaction, dermatitis acneiform, seborrheic dermatitis, palmar-plantar erythrodysesthesia syndrome, rash generalized] | 21 | 0.5
Pruritus | 19 | 0.3
Edema peripheral [Includes edema peripheral, peripheral swelling] | 14 | 1.1
Infections
Urinary tract infection | 19 | 9
Blood and Lymphatic System
Anemia | 17 | 7
Respiratory, Thoracic, and Mediastinal
Cough | 14 | 0
Dyspnea | 11 | 0.5
Renal and Urinary
Increased blood creatinine | 11 | 1.1
Hematuria | 13 | 3.0

Previously Treated Urothelial Carcinoma

The safety of intravenous pembrolizumab for the treatment of patients with locally advanced or metastatic urothelial carcinoma with disease progression following platinum-containing chemotherapy was investigated in KEYNOTE-045. KEYNOTE-045 was a multicenter, open-label, randomized (1:1), active-controlled trial in which 266 patients received intravenous pembrolizumab 200 mg every 3 weeks or investigator's choice of chemotherapy (n=255), consisting of paclitaxel (n=84), docetaxel (n=84) or vinflunine (n=87) [see Clinical Studies (14.6)]. Patients with autoimmune disease or a medical condition that required systemic corticosteroids or other immunosuppressive medications were ineligible.

The median duration of exposure was 3.5 months (range: 1 day to 20 months) in patients who received intravenous pembrolizumab and 1.5 months (range: 1 day to 14 months) in patients who received chemotherapy.

Intravenous pembrolizumab was discontinued due to adverse reactions in 8% of patients. The most common adverse reaction resulting in permanent discontinuation of intravenous pembrolizumab was pneumonitis (1.9%). Adverse reactions leading to interruption of intravenous pembrolizumab occurred in 20% of patients; the most common (≥1%) were urinary tract infection (1.5%), diarrhea (1.5%), and colitis (1.1%). Serious adverse reactions occurred in 39% of intravenous pembrolizumab-treated patients. The most frequent serious adverse reactions (≥2%) in intravenous pembrolizumab-treated patients were urinary tract infection, pneumonia, anemia, and pneumonitis. Tables 27 and 28 summarize adverse reactions and laboratory abnormalities, respectively, in patients on intravenous pembrolizumab in KEYNOTE-045.

Table 27: Adverse Reactions Occurring in ≥10% of Patients Receiving Intravenous Pembrolizumab in KEYNOTE-045
Adverse Reaction | Intravenous Pembrolizumab 200 mg every 3 weeks n=266 |  | Chemotherapy [Chemotherapy: paclitaxel, docetaxel, or vinflunine] n=255
Adverse Reaction | All Grades [Graded per NCI CTCAE v4.0] (%) | Grades 3-4 (%) | All Grades (%) | Grades 3-4 (%)
General
Fatigue [Includes asthenia, fatigue, malaise, lethargy] | 38 | 4.5 | 56 | 11
Pyrexia | 14 | 0.8 | 13 | 1.2
Musculoskeletal and Connective Tissue
Musculoskeletal pain [Includes back pain, myalgia, bone pain, musculoskeletal pain, pain in extremity, musculoskeletal chest pain, musculoskeletal discomfort, neck pain] | 32 | 3.0 | 27 | 2.0
Skin and Subcutaneous Tissue
Pruritus | 23 | 0 | 6 | 0.4
Rash [Includes rash maculo-papular, rash, genital rash, rash erythematous, rash papular, rash pruritic, rash pustular, erythema, drug eruption, eczema, eczema asteatotic, dermatitis contact, dermatitis acneiform, dermatitis, seborrheic keratosis, lichenoid keratosis] | 20 | 0.4 | 13 | 0.4
Gastrointestinal
Nausea | 21 | 1.1 | 29 | 1.6
Constipation | 19 | 1.1 | 32 | 3.1
Diarrhea [Includes diarrhea, gastroenteritis, colitis, enterocolitis] | 18 | 2.3 | 19 | 1.6
Vomiting | 15 | 0.4 | 13 | 0.4
Abdominal pain | 13 | 1.1 | 13 | 2.7
Metabolism and Nutrition
Decreased appetite | 21 | 3.8 | 21 | 1.2
Infections
Urinary tract infection | 15 | 4.9 | 14 | 4.3
Respiratory, Thoracic and Mediastinal
Cough [Includes cough, productive cough] | 15 | 0.4 | 9 | 0
Dyspnea [Includes dyspnea, dyspnea exertional, wheezing] | 14 | 1.9 | 12 | 1.2
Renal and Urinary
Hematuria [Includes blood urine present, hematuria, chromaturia] | 12 | 2.3 | 8 | 1.6

Table 28: Laboratory Abnormalities Worsened from Baseline Occurring in ≥20% of Urothelial Carcinoma Patients Receiving Intravenous Pembrolizumab in KEYNOTE-045
Laboratory Test [Each test incidence is based on the number of patients who had both baseline and at least one on-study laboratory measurement available: intravenous pembrolizumab (range: 240 to 248 patients) and chemotherapy (range: 238 to 244 patients); phosphate decreased: intravenous pembrolizumab n=232 and chemotherapy n=222.] | Intravenous Pembrolizumab 200 mg every 3 weeks |  | Chemotherapy
Laboratory Test [Each test incidence is based on the number of patients who had both baseline and at least one on-study laboratory measurement available: intravenous pembrolizumab (range: 240 to 248 patients) and chemotherapy (range: 238 to 244 patients); phosphate decreased: intravenous pembrolizumab n=232 and chemotherapy n=222.] | All Grades [Graded per NCI CTCAE v4.0] % | Grades 3-4 % | All Grades % | Grades 3-4 %
Chemistry
Hyperglycemia | 52 | 8 | 60 | 7
Anemia | 52 | 13 | 68 | 18
Lymphopenia | 45 | 15 | 55 | 26
Hypoalbuminemia | 43 | 1.7 | 50 | 3.8
Hyponatremia | 37 | 9 | 47 | 13
Increased alkaline phosphatase | 37 | 7 | 33 | 4.9
Increased creatinine | 35 | 4.4 | 28 | 2.9
Hypophosphatemia | 29 | 8 | 34 | 14
Increased AST | 28 | 4.1 | 20 | 2.5
Hyperkalemia | 28 | 0.8 | 27 | 6
Hypocalcemia | 26 | 1.6 | 34 | 2.1

Neoadjuvant and Adjuvant Treatment of Cisplatin-Ineligible Patients with MIBC in Combination with Enfortumab Vedotin

The safety of intravenous pembrolizumab in combination with enfortumab vedotin as neoadjuvant treatment and continued after radical cystectomy (RC) as adjuvant treatment was investigated in KEYNOTE-905, an open-label, multicenter, randomized, active-controlled trial in patients with previously untreated MIBC who were ineligible for or declined cisplatin-based chemotherapy. Patients received intravenous pembrolizumab in combination with enfortumab vedotin (n=167) before and after RC with pelvic lymph node dissection (PLND) or RC with PLND alone (n=159) [see Clinical Studies (14.7)].

For the 167 patients who received intravenous pembrolizumab in the neoadjuvant phase, the median duration of exposure to intravenous pembrolizumab 200 mg every 3 weeks was 1.4 months (range: 1 day to 2.7 months) and the median number of cycles of intravenous pembrolizumab was 3 (range: 1 to 3) out of the planned 3 cycles in the neoadjuvant phase. For the 96 patients who received intravenous pembrolizumab in the adjuvant phase, the median duration of exposure to intravenous pembrolizumab 200 mg every 3 weeks was 8.5 months (range: 1 day to 12.9 months) and the median number of cycles of intravenous pembrolizumab was 12 (range: 1 to 14) out of the planned 14 cycles in the adjuvant phase. Across the combined neoadjuvant and adjuvant phases (n=167), the median number of cycles of intravenous pembrolizumab was 5 (range: 1 to 17) out of the planned 17 cycles.

Tables 29 and 30 summarize adverse reactions and laboratory abnormalities, respectively, in patients on intravenous pembrolizumab in combination with enfortumab vedotin in KEYNOTE-905.

Table 29: Adverse Reactions ≥20% (All Grades) in Patients Treated with Intravenous Pembrolizumab in Combination with Enfortumab Vedotin in KEYNOTE-905
Adverse Reaction | Intravenous Pembrolizumab 200 mg every 3 weeks in combination with enfortumab vedotin before and after RC with PLND n=167 |  | RC with PLND alone n=159
Adverse Reaction | All Grades % | Grade 3-4 % | All Grades % | Grade 3-4 %
Skin and subcutaneous tissue disorders
Rash [Includes multiple terms.] , [Includes rash, rash maculo-papular, conjunctivitis, erythema, eczema, skin exfoliation, palmar-plantar erythrodysesthesia syndrome, blister, dermatitis, dermatitis exfoliative generalized, exfoliative rash, rash papular, rash pruritic, dermatitis bullous, drug eruption, pemphigoid, rash vesicular, and dermatitis contact.] | 54 | 7 | 1.3 | 0
Pruritus | 47 | 3 | 0 | 0
Alopecia | 35 | 0.6 | 0 | 0
General disorders and administration site conditions
Fatigue | 47 | 4.2 | 6 | 0.6
Nervous system disorders
Peripheral neuropathy | 39 | 3 | 1.9 | 0
Dysgeusia | 35 | 0 | 0 | 0
Gastrointestinal disorders
Diarrhea | 34 | 5 | 3.1 | 1.3
Constipation | 28 | 1.8 | 8 | 0
Nausea | 26 | 1.2 | 8 | 0.6
Metabolism and nutrition disorders
Decreased appetite | 28 | 0.6 | 1.9 | 0
Infections and infestations
Urinary tract infection | 24 | 12 | 13 | 11
Eye disorders
Dry eye | 21 | 0 | 0 | 0
Investigations
Weight loss | 20 | 0 | 3.1 | 0

Clinically relevant adverse reactions (<20%) include dry skin (15%), hypothyroidism (14%), vomiting (9%), pneumonitis/ILD (4.2%), skin hyperpigmentation (3.0%), infusion site extravasation (1.2%), and myasthenia gravis and myositis (0.6% each).

Table 30: Selected Laboratory Abnormalities Worsened from Baseline Occurring in ≥20% of Patients Treated with Intravenous Pembrolizumab in Combination with Enfortumab Vedotin in KEYNOTE-905
Laboratory Test [Each test incidence is based on the number of patients who had both baseline and at least one on-study laboratory measurement available: Intravenous pembrolizumab in combination with enfortumab vedotin (167 patients), and RC and PLND alone (range: 110 to 121 patients).] | Intravenous Pembrolizumab 200 mg every 3 weeks in combination with enfortumab vedotin before and after RC with PLND n=167 |  | RC with PLND alone n=159
Laboratory Test [Each test incidence is based on the number of patients who had both baseline and at least one on-study laboratory measurement available: Intravenous pembrolizumab in combination with enfortumab vedotin (167 patients), and RC and PLND alone (range: 110 to 121 patients).] | All Grades [Graded per NCI CTCAE v4.03] % | Grades 3-4 % | All Grades % | Grades 3-4 %
Chemistry
Increased glucose | 72 | 12 | 24 | 1.7
Increased AST | 55 | 6 | 11 | 1.8
Increased ALT | 53 | 4.8 | 13 | 0.9
Increased creatinine | 47 | 8 | 31 | 2.5
Decreased sodium | 44 | 13 | 18 | 7
Increased potassium | 39 | 7 | 20 | 6
Decreased phosphate | 26 | 6 | 1.8 | 0
Hematology
Decreased hemoglobin | 60 | 13 | 48 | 8
Decreased lymphocytes | 40 | 8 | 17 | 1.7
ALT = alanine aminotransferase; AST = aspartate aminotransferase.

Neoadjuvant Phase of KEYNOTE-905

A total of 167 patients received at least 1 dose of intravenous pembrolizumab in combination with enfortumab vedotin as neoadjuvant treatment before receiving RC.

In the neoadjuvant phase, serious adverse reactions occurred in 27% of patients receiving intravenous pembrolizumab in combination with enfortumab vedotin. The most frequent (≥2%) serious adverse reactions were urinary tract infection (3.6%) and hematuria (2.4%). Fatal adverse reactions occurred in 1.2% of patients, including myasthenia gravis and toxic epidermal necrolysis (0.6% each). Additional fatal adverse reactions were reported in 2.7% of patients in the post-surgery phase before adjuvant treatment started, including sepsis and intestinal obstruction (1.4% each).

Permanent discontinuation of intravenous pembrolizumab due to an adverse reaction occurred in 15% of patients. The most frequent (>1%) adverse reactions resulting in permanent discontinuation of intravenous pembrolizumab were rash (2.4%, including generalized exfoliative dermatitis), increased alanine aminotransferase, increased aspartate aminotransferase, diarrhea, dysgeusia, and toxic epidermal necrolysis (1.2% each).

Adverse reactions leading to dose interruption of intravenous pembrolizumab in the neoadjuvant phase occurred in 20% of patients. The most common adverse reactions (≥2%) leading to dose interruption of intravenous pembrolizumab were rash (4.8%) and neutropenia (2.4%). Of the 167 patients in the intravenous pembrolizumab in combination with enfortumab vedotin arm who received neoadjuvant treatment, 7 (4.2%) patients did not receive surgery due to adverse reactions. The adverse reactions that led to cancellation of surgery were acute myocardial infarction, bile duct cancer, colon cancer, respiratory distress, urinary tract infection, and the two deaths due to myasthenia gravis and toxic epidermal necrolysis (0.6% each).

Of the 146 patients who received neoadjuvant treatment with intravenous pembrolizumab in combination with enfortumab vedotin and underwent radical cystectomy, 6 (4.1%) patients experienced delay of surgery (defined as time from last neoadjuvant treatment to surgery exceeding 8 weeks) due to adverse reactions.

Adjuvant Phase of KEYNOTE-905

Patients who did not proceed to surgery were ineligible for adjuvant therapy. Of the 149 patients who underwent surgery, 100 patients received adjuvant treatment with intravenous pembrolizumab in combination with enfortumab vedotin. Of the 49 patients who did not receive adjuvant treatment, discontinuation of treatment prior to the adjuvant phase was due to an adverse event in 21 patients.

In the adjuvant phase, serious adverse reactions occurred in 43% of patients; the most frequent (≥2%) serious adverse reactions were urinary tract infection (8%), acute kidney injury and pyelonephritis (5% each), urosepsis (4%), and hypokalemia, intestinal obstruction, and sepsis (2% each). Fatal adverse reactions occurred in 7% of patients, including urosepsis, intracranial hemorrhage, death, myocardial infarction, multiple organ dysfunction syndrome, and pseudomonal pneumonia (1% each).

Permanent discontinuation of intravenous pembrolizumab due to an adverse reaction occurred in 28% of patients. The most frequent (>1%) adverse reactions resulting in permanent discontinuation of intravenous pembrolizumab were diarrhea (5%), and peripheral neuropathy, acute kidney injury, and pneumonitis (2% each).

Adverse reactions leading to dose interruption of intravenous pembrolizumab in the adjuvant phase occurred in 38% of patients. The most common adverse reactions (≥2%) leading to dose interruption of intravenous pembrolizumab were rash (7%), urinary tract infection (6%), diarrhea (4%), and abdominal pain, COVID-19, fatigue, pruritus, and pyelonephritis (2% each).

BCG-unresponsive High-risk NMIBC

The safety of intravenous pembrolizumab was investigated in KEYNOTE-057, a multicenter, open-label, single-arm trial that enrolled 148 patients with high-risk non-muscle invasive bladder cancer (NMIBC), 96 of whom had BCG-unresponsive carcinoma in situ (CIS) with or without papillary tumors. Patients received intravenous pembrolizumab 200 mg every 3 weeks until unacceptable toxicity, persistent or recurrent high-risk NMIBC or progressive disease, or up to 24 months of therapy without disease progression.

The median duration of exposure to intravenous pembrolizumab was 4.3 months (range: 1 day to 25.6 months).

Intravenous pembrolizumab was discontinued due to adverse reactions in 11% of patients. The most common adverse (>1%) reaction resulting in permanent discontinuation of intravenous pembrolizumab was pneumonitis (1.4%). Adverse reactions leading to interruption of intravenous pembrolizumab occurred in 22% of patients; the most common (≥2%) were diarrhea (4%) and urinary tract infection (2%). Serious adverse reactions occurred in 28% of intravenous pembrolizumab-treated patients. The most frequent serious adverse reactions (≥2%) in intravenous pembrolizumab-treated patients were pneumonia (3%), cardiac ischemia (2%), colitis (2%), pulmonary embolism (2%), sepsis (2%), and urinary tract infection (2%). Tables 31 and 32 summarize adverse reactions and laboratory abnormalities, respectively, in patients on intravenous pembrolizumab in KEYNOTE-057.

Table 31: Adverse Reactions Occurring in ≥10% of Patients Receiving Intravenous Pembrolizumab in KEYNOTE-057
Adverse Reaction | Intravenous Pembrolizumab 200 mg every 3 weeks N=148
Adverse Reaction | All Grades [Graded per NCI CTCAE v4.03] (%) | Grades 3–4 (%)
General
Fatigue [Includes asthenia, fatigue, malaise] | 29 | 0.7
Peripheral edema [Includes edema peripheral, peripheral swelling] | 11 | 0
Gastrointestinal
Diarrhea [Includes diarrhea, gastroenteritis, colitis] | 24 | 2.0
Nausea | 13 | 0
Constipation | 12 | 0
Skin and Subcutaneous Tissue
Rash [Includes rash maculo-papular, rash, rash erythematous, rash pruritic, rash pustular, erythema, eczema, eczema asteatotic, lichenoid keratosis, urticaria, dermatitis] | 24 | 0.7
Pruritus | 19 | 0.7
Musculoskeletal and Connective Tissue
Musculoskeletal pain [Includes back pain, myalgia, musculoskeletal pain, pain in extremity, musculoskeletal chest pain, neck pain] | 19 | 0
Arthralgia | 14 | 1.4
Renal and Urinary
Hematuria | 19 | 1.4
Respiratory, Thoracic, and Mediastinal
Cough [Includes cough, productive cough] | 19 | 0
Infections
Urinary tract infection | 12 | 2.0
Nasopharyngitis | 10 | 0
Endocrine
Hypothyroidism | 11 | 0

Table 32: Laboratory Abnormalities Worsened from Baseline Occurring in ≥20% of BCG-unresponsive NMIBC Patients Receiving Intravenous Pembrolizumab in KEYNOTE-057
Laboratory Test [Each test incidence is based on the number of patients who had both baseline and at least one on-study laboratory measurement available: intravenous pembrolizumab (range: 124 to 147 patients)] | Intravenous Pembrolizumab 200 mg every 3 weeks
Laboratory Test [Each test incidence is based on the number of patients who had both baseline and at least one on-study laboratory measurement available: intravenous pembrolizumab (range: 124 to 147 patients)] | All Grades [Graded per NCI CTCAE v4.03] (%) | Grades 3-4 (%)
Chemistry
Hyperglycemia | 59 | 7
Increased ALT | 25 | 2.7
Hyponatremia | 24 | 7
Hypophosphatemia | 24 | 6
Hypoalbuminemia | 24 | 1.4
Hyperkalemia | 23 | 1.4
Hypocalcemia | 22 | 0.7
Increased AST | 20 | 2.7
Increased creatinine | 20 | 0.7
Hematology
Anemia | 35 | 1.4
Lymphopenia | 29 | 1.6

Microsatellite Instability-High or Mismatch Repair Deficient Cancer

The safety of intravenous pembrolizumab was investigated in 504 patients with MSI-H or dMMR cancer enrolled in KEYNOTE-158, KEYNOTE-164, and KEYNOTE-051 [see Clinical Studies (14.7)]. The median duration of exposure to intravenous pembrolizumab was 6.2 months (range: 1 day to 53.5 months). Adverse reactions occurring in patients with MSI-H or dMMR cancer were similar to those occurring in patients with other solid tumors who received intravenous pembrolizumab as a single agent.

Microsatellite Instability-High or Mismatch Repair Deficient Colorectal Cancer

Among the 153 patients with MSI-H or dMMR CRC enrolled in KEYNOTE-177 [see Clinical Studies (14.8)] treated with intravenous pembrolizumab, the median duration of exposure to intravenous pembrolizumab was 11.1 months (range: 1 day to 30.6 months). Patients with autoimmune disease or a medical condition that required immunosuppression were ineligible. Adverse reactions occurring in patients with MSI-H or dMMR CRC were similar to those occurring in 2799 patients with melanoma or NSCLC treated with intravenous pembrolizumab as a single agent.

Gastric Cancer

First-line Treatment of Locally Advanced Unresectable or Metastatic HER2-Positive Gastric or Gastroesophageal Junction Adenocarcinoma

The safety of intravenous pembrolizumab was evaluated in 696 patients with HER2-positive gastric or GEJ cancer enrolled in KEYNOTE-811, which included 350 patients treated with intravenous pembrolizumab 200 mg, trastuzumab, and CAPOX (n=297) or FP (n=53) every 3 weeks, compared to 346 patients treated with placebo, trastuzumab, and CAPOX (n=298) or FP (n=48) every 3 weeks [see Clinical Studies (14.10)].

The median duration of exposure to intravenous pembrolizumab was 9.2 months (range: 1 day to 33.6 months).

Fatal adverse reactions occurred in 3 patients who received intravenous pembrolizumab in combination with trastuzumab and CAPOX or FP and included pneumonitis in 2 patients and hepatitis in 1 patient.

Intravenous pembrolizumab was discontinued due to adverse reactions in 13% of patients. Adverse reactions resulting in permanent discontinuation of intravenous pembrolizumab in ≥1% of patients were pneumonitis (2.0%) and pneumonia (1.1%).

Adverse reactions leading to interruption of intravenous pembrolizumab occurred in 71% of patients; the most common adverse reactions or laboratory abnormalities leading to interruption of intravenous pembrolizumab (≥2%) were neutropenia (21%), thrombocytopenia (13%), diarrhea (7%), pneumonia (5%), anemia (4.9%), COVID-19 (3.1%), hypokalemia (3.1%), fatigue/asthenia (4.9%), decreased appetite (4%), increased AST (3.7%), increased blood bilirubin (4.6%), increased ALT (2.9%), vomiting (2.6%), pneumonitis (2.3%), pyrexia (2.3%), increased blood creatinine (2%), and colitis (2%).

In the intravenous pembrolizumab arm versus placebo, there was a difference of ≥5% incidence between patients treated with intravenous pembrolizumab versus standard of care for diarrhea (53% vs. 47%), rash (35% vs. 28%), hypothyroidism (11% vs. 5%), and pneumonia (11% vs. 5%). There were no clinically meaningful differences in incidence of Grade 3-4 toxicity between arms.

There was a difference of ≥5% incidence between patients treated with intravenous pembrolizumab versus standard of care for decreased leukocytes (60% vs. 54%), decreased calcium (56% vs. 46%), decreased lymphocytes (59% vs. 51%), decreased potassium (41% vs. 36%), increased bilirubin (33% vs. 25%), increased creatinine (28% vs. 18%), and decreased glucose (17% vs. 11%). There were no clinically meaningful differences in incidence of Grade 3-4 toxicity between arms.

First-line Treatment of Locally Advanced Unresectable or Metastatic HER2-Negative Gastric or Gastroesophageal Junction Adenocarcinoma

The safety of intravenous pembrolizumab was evaluated in 1572 patients with HER2-negative gastric or GEJ cancer enrolled in KEYNOTE-859, which included 785 patients treated with intravenous pembrolizumab 200 mg and FP (n=106) or CAPOX (n=674) every 3 weeks, compared to 787 patients who received placebo and FP (n=107) or CAPOX (n=679) every 3 weeks [see Clinical Studies (14.9)].

The median duration of exposure to intravenous pembrolizumab was 6.2 months (range: 1 day to 33.7 months).

Serious adverse reactions occurred in 45% of patients receiving intravenous pembrolizumab. Serious adverse reactions in >2% of patients included pneumonia (4.1%), diarrhea (3.9%), hemorrhage (3.9%), and vomiting (2.4%). Fatal adverse reactions occurred in 8% of patients who received intravenous pembrolizumab, including infection (2.3%) and thromboembolism (1.3%).

Permanent discontinuation of intravenous pembrolizumab due to adverse reactions occurred in 15% of patients. Adverse reaction resulting in permanent discontinuation of intravenous pembrolizumab in ≥1% were infections (1.8%) and diarrhea (1.0%).

Dosage interruptions of intravenous pembrolizumab due to an adverse reaction occurred in 65% of patients. Adverse reactions or laboratory abnormalities leading to interruption of intravenous pembrolizumab (≥2%) were neutropenia (21%), thrombocytopenia (13%), diarrhea (5.5%), fatigue (4.8%), infection (4.8%), anemia (4.5%), increased AST (4.3%), increased ALT (3.8%), increased blood bilirubin (3.3%), white blood cell count decreased (2.2%), nausea (2%), palmar-plantar erythrodysesthesia syndrome (2%), and vomiting (2%).

Tables 33 and 34 summarize adverse reactions and laboratory abnormalities, respectively, in patients on intravenous pembrolizumab in KEYNOTE-859.

Table 33: Adverse Reactions Occurring in ≥20% of Patients Receiving Intravenous Pembrolizumab in KEYNOTE-859
Adverse Reaction | Intravenous Pembrolizumab 200 mg every 3 weeks and FP or CAPOX n=785 |  | Placebo and FP or CAPOX n=787
Adverse Reaction | All Grades [Graded per NCI CTCAE v4.03] (%) | Grades 3-4 (%) | All Grades (%) | Grades 3-4 (%)
Nervous System
Peripheral neuropathy [Includes dysesthesia, hyperesthesia, hypoesthesia, neuralgia, neuropathy peripheral, paresthesia, peripheral sensory neuropathy, peripheral motor neuropathy, polyneuropathy] | 47 | 5 | 48 | 6
Gastrointestinal
Nausea | 46 | 3.7 | 46 | 4.4
Diarrhea | 36 | 6 | 32 | 5
Vomiting | 34 | 5 | 27 | 5
Abdominal Pain [Includes abdominal discomfort, abdominal pain, abdominal pain lower, abdominal tenderness, abdominal pain upper, epigastric discomfort, gastrointestinal pain] | 26 | 2.8 | 24 | 2.9
Constipation | 22 | 0.5 | 21 | 0.8
General
Fatigue [Includes asthenia, fatigue] | 40 | 8 | 39 | 9
Metabolism and Nutrition
Decreased appetite | 29 | 3.3 | 29 | 2.5
Skin and Subcutaneous Tissue
Palmar-plantar erythrodysesthesia syndrome | 25 | 3.1 | 22 | 1.8
Investigations
Weight loss | 20 | 2.8 | 19 | 2.7

Table 34: Laboratory Abnormalities Worsened from Baseline Occurring in ≥20% of Patients Receiving Intravenous Pembrolizumab in KEYNOTE-859
Laboratory Test [Each test incidence is based on the number of patients who had both baseline and at least one on-study laboratory measurement available: intravenous pembrolizumab/FP or CAPOX (range: 210 to 766 patients) and placebo/FP or CAPOX (range: 190 to 762 patients)] | Intravenous Pembrolizumab 200 mg every 3 weeks and FP or CAPOX |  | Placebo and FP or CAPOX
Laboratory Test [Each test incidence is based on the number of patients who had both baseline and at least one on-study laboratory measurement available: intravenous pembrolizumab/FP or CAPOX (range: 210 to 766 patients) and placebo/FP or CAPOX (range: 190 to 762 patients)] | All Grades [Graded per NCI CTCAE v4.03] % | Grades 3-4 % | All Grades % | Grades 3-4 %
Hematology
Anemia | 65 | 15 | 69 | 13
Thrombocytopenia | 64 | 12 | 62 | 10
Neutropenia | 63 | 25 | 58 | 20
Leukopenia | 59 | 7 | 56 | 6
Lymphopenia | 57 | 20 | 51 | 16
Chemistry
Increased AST | 57 | 4.7 | 48 | 3.6
Hypoalbuminemia | 55 | 4.1 | 52 | 2.9
Hyperglycemia | 53 | 6 | 52 | 4.6
Hypocalcemia | 49 | 3.6 | 45 | 3.3
Increased alkaline phosphatase | 48 | 6 | 41 | 5
Hyponatremia | 40 | 13 | 40 | 12
Increased ALT | 40 | 4.2 | 29 | 2.9
Hypokalemia | 35 | 10 | 27 | 9
Bilirubin increased | 32 | 5 | 30 | 5
Hypophosphatemia | 30 | 10 | 27 | 8
Hypomagnesemia | 29 | 0.3 | 22 | 0.7
Increased creatinine | 21 | 3.5 | 18 | 1.7
Hyperkalemia | 20 | 3.7 | 18 | 2.9
Increased INR | 20 | 1.4 | 22 | 0

Esophageal Cancer

First-line Treatment of Locally Advanced Unresectable or Metastatic Esophageal Cancer/Gastroesophageal Junction

The safety of intravenous pembrolizumab, in combination with cisplatin and FU chemotherapy was investigated in KEYNOTE-590, a multicenter, double-blind, randomized (1:1), placebo-controlled trial for the first-line treatment in patients with metastatic or locally advanced esophageal or gastroesophageal junction (tumors with epicenter 1 to 5 centimeters above the GEJ) carcinoma who were not candidates for surgical resection or definitive chemoradiation [see Clinical Studies (14.10)]. A total of 740 patients received either intravenous pembrolizumab 200 mg (n=370) or placebo (n=370) every 3 weeks for up to 35 cycles, both in combination with up to 6 cycles of cisplatin and up to 35 cycles of FU.

The median duration of exposure was 5.7 months (range: 1 day to 26 months) in the intravenous pembrolizumab combination arm and 5.1 months (range: 3 days to 27 months) in the chemotherapy arm.

Intravenous pembrolizumab was discontinued for adverse reactions in 15% of patients. The most common adverse reactions resulting in permanent discontinuation of intravenous pembrolizumab (≥1%) were pneumonitis (1.6%), acute kidney injury (1.1%), and pneumonia (1.1%). Adverse reactions leading to interruption of intravenous pembrolizumab occurred in 67% of patients. The most common adverse reactions leading to interruption of intravenous pembrolizumab (≥2%) were neutropenia (19%), fatigue/asthenia (8%), decreased white blood cell count (5%), pneumonia (5%), decreased appetite (4.3%), anemia (3.2%), increased blood creatinine (3.2%), stomatitis (3.2%), malaise (3.0%), thrombocytopenia (3%), pneumonitis (2.7%), diarrhea (2.4%), dysphagia (2.2%), and nausea (2.2%).

Tables 35 and 36 summarize adverse reactions and laboratory abnormalities, respectively, in patients on intravenous pembrolizumab in KEYNOTE-590.

Table 35: Adverse Reactions Occurring in ≥20% of Patients Receiving Intravenous Pembrolizumab in KEYNOTE-590
Adverse Reaction | Intravenous Pembrolizumab 200 mg every 3 weeks Cisplatin FU n=370 |  | Placebo Cisplatin FU n=370
Adverse Reaction | All Grades [Graded per NCI CTCAE v4.03] (%) | Grades 3-4 [One fatal event of diarrhea was reported in each arm.] (%) | All Grades (%) | Grades 3-4 (%)
Gastrointestinal
Nausea | 67 | 7 | 63 | 7
Constipation | 40 | 0 | 40 | 0
Diarrhea | 36 | 4.1 | 33 | 3
Vomiting | 34 | 7 | 32 | 5
Stomatitis | 27 | 6 | 26 | 3.8
General
Fatigue [Includes asthenia, fatigue] | 57 | 12 | 46 | 9
Metabolism and Nutrition
Decreased appetite | 44 | 4.1 | 38 | 5
Investigations
Weight loss | 24 | 3.0 | 24 | 5

Table 36: Laboratory Abnormalities Worsened from Baseline Occurring in ≥20% of Esophageal Cancer Patients Receiving Intravenous Pembrolizumab in KEYNOTE-590
Laboratory Test [Each test incidence is based on the number of patients who had both baseline and at least one on-study laboratory measurement available: intravenous pembrolizumab/cisplatin/FU (range: 353 to 365 patients) and placebo/cisplatin/FU (range: 347 to 359 patients)] | Intravenous Pembrolizumab 200 mg every 3 weeks Cisplatin FU |  | Chemotherapy (Cisplatin and FU)
Laboratory Test [Each test incidence is based on the number of patients who had both baseline and at least one on-study laboratory measurement available: intravenous pembrolizumab/cisplatin/FU (range: 353 to 365 patients) and placebo/cisplatin/FU (range: 347 to 359 patients)] | All Grades [Graded per NCI CTCAE v4.03] % | Grades 3-4 % | All Grades % | Grades 3-4 %
Hematology
Anemia | 84 | 21 | 87 | 25
Neutropenia | 77 | 44 | 73 | 41
Leukopenia | 73 | 21 | 73 | 17
Lymphopenia | 57 | 23 | 53 | 18
Thrombocytopenia | 43 | 5 | 46 | 8
Chemistry
Hyperglycemia | 56 | 7 | 55 | 6
Hyponatremia | 53 | 19 | 53 | 19
Hypoalbuminemia | 53 | 2.8 | 52 | 2.3
Increased creatinine | 45 | 2.5 | 42 | 2.5
Hypocalcemia | 44 | 3.9 | 37 | 2
Hypophosphatemia | 37 | 9 | 31 | 10
Hypokalemia | 30 | 12 | 34 | 15
Increased alkaline phosphatase | 29 | 1.9 | 29 | 1.7
Hyperkalemia | 28 | 3.6 | 28 | 2.5
Increased AST | 25 | 4.4 | 22 | 2.8
Increased ALT | 23 | 3.6 | 18 | 1.7

Previously Treated Recurrent Locally Advanced or Metastatic Esophageal Cancer

Among the 314 patients with esophageal cancer enrolled in KEYNOTE-181 [see Clinical Studies (14.10)] treated with intravenous pembrolizumab, the median duration of exposure to intravenous pembrolizumab was 2.1 months (range: 1 day to 24.4 months). Patients with autoimmune disease or a medical condition that required immunosuppression were ineligible. Adverse reactions occurring in patients with esophageal cancer were similar to those occurring in 2799 patients with melanoma or NSCLC treated with intravenous pembrolizumab as a single agent.

Cervical Cancer

FIGO 2014 Stage III-IVA Cervical Cancer with Chemoradiotherapy

The safety of intravenous pembrolizumab in combination with CRT (cisplatin plus external beam radiation therapy [EBRT] followed by brachytherapy [BT]) was investigated in KEYNOTE-A18, a placebo-controlled, randomized (1:1), multicenter, double-blind trial including 597 patients with FIGO 2014 Stage III-IVA cervical cancer [see Clinical Studies (14.11)]. Two hundred ninety-four patients received intravenous pembrolizumab in combination with chemoradiotherapy and 303 patients received placebo in combination with chemoradiotherapy.

The median duration of exposure to intravenous pembrolizumab was 20 months (range: 1 day to 32 months).

Fatal adverse reactions occurred in 1.4% of patients receiving intravenous pembrolizumab in combination with chemoradiotherapy, including 1 case each (0.3%) of large intestinal perforation, urosepsis, sepsis, and vaginal hemorrhage.

Serious adverse reactions occurred in 34% of patients receiving intravenous pembrolizumab in combination with chemoradiotherapy. Serious adverse reactions occurring in ≥1% of patients included urinary tract infection (3.1%), urosepsis (1.4%), and sepsis (1%).

Intravenous pembrolizumab was discontinued for adverse reactions in 9% of patients. The most common adverse reaction (≥1%) resulting in permanent discontinuation was diarrhea (1%).

Adverse reactions leading to interruption of intravenous pembrolizumab occurred in 47% of patients; the most common adverse reactions leading to interruption of intravenous pembrolizumab (≥2%) were anemia (7%), COVID-19 (7%), SARS-CoV-2 test positive (4.8%), diarrhea (4.1%), increased ALT (4.1%), increased AST (3.4%) decreased neutrophil count (3.1%), and urinary tract infection (2.7%).

Table 37 and Table 38 summarize adverse reactions and laboratory abnormalities, respectively, in patients on intravenous pembrolizumab in KEYNOTE-A18.

Table 37: Adverse Reactions Occurring in ≥10% of Patients with FIGO 2014 Stage III-IVA Cervical Cancer Receiving Intravenous Pembrolizumab in KEYNOTE-A18
Adverse Reaction | Intravenous Pembrolizumab 200 mg every 3 weeks and 400 mg every 6 weeks with chemoradiotherapy n=294 |  | Placebo with chemoradiotherapy n=303
Adverse Reaction | All Grades [Graded per NCI CTCAE v5.0] (%) | Grades 3-4 (%) | All Grades (%) | Grades 3-4 (%)
Gastrointestinal
Nausea | 56 | 0 | 62 | 2.3
Diarrhea | 51 | 4.4 | 50 | 4.3
Vomiting | 34 | 1.0 | 35 | 1.7
Constipation | 20 | 0 | 19 | 0.7
Abdominal pain | 13 | 1.0 | 14 | 1.7
Infections
Urinary tract infection [Includes urinary tract infection, urinary tract infection pseudomonal, pyelonephritis acute, cystitis, Escherichia urinary tract infection] | 35 | 4.8 | 34 | 5
COVID-19 | 10 | 0 | 7 | 1.0
General
Fatigue [Includes fatigue, asthenia] | 28 | 1.0 | 28 | 1.3
Pyrexia | 14 | 0.7 | 15 | 0
Endocrine
Hypothyroidism [Includes hypothyroidism, autoimmune hypothyroidism] | 23 | 0.7 | 8 | 0
Hyperthyroidism | 13 | 0.3 | 3.3 | 0
Investigations
Weight loss | 19 | 2.4 | 19 | 1.0
Metabolism and Nutrition
Decreased appetite | 18 | 0.7 | 17 | 0.3
Renal and Urinary
Dysuria | 12 | 0.3 | 12 | 0
Skin and Subcutaneous Tissue Disorders
Rash [Includes erythema multiforme, dermatitis, drug eruption, eczema, rash, skin exfoliation, dermatitis bullous, rash maculo-papular, lichen planus, dyshidrotic eczema, dermatitis acneiform] | 12 | 1.0 | 8 | 0.3
Musculoskeletal and Connective Tissues Disorders
Back pain | 11 | 0.7 | 11 | 0.7
Reproductive System
Pelvic pain | 11 | 1.0 | 14 | 1.7

Table 38: Laboratory Abnormalities Worsened from Baseline Occurring in ≥20% of Patients with FIGO 2014 Stage III-IVA Cervical Cancer Receiving Intravenous Pembrolizumab in KEYNOTE-A18
Laboratory Test [Laboratory abnormality percentage is based on the number of patients who had both baseline and at least one post-baseline laboratory measurement for each parameter: Intravenous pembrolizumab + chemoradiotherapy (range: 288 to 293 patients) and placebo + chemoradiotherapy (range: 299 to 301 patients)] | Intravenous Pembrolizumab 200 mg every 3 weeks and 400 mg every 6 weeks with chemoradiotherapy |  | Placebo with chemoradiotherapy
Laboratory Test [Laboratory abnormality percentage is based on the number of patients who had both baseline and at least one post-baseline laboratory measurement for each parameter: Intravenous pembrolizumab + chemoradiotherapy (range: 288 to 293 patients) and placebo + chemoradiotherapy (range: 299 to 301 patients)] | All Grades [Graded per NCI CTCAE v5.0] (%) | Grades 3-4 (%) | All Grades (%) | Grades 3-4 (%)
Hematology
Lymphopenia | 99 | 96 | 99 | 92
Leukopenia | 96 | 48 | 94 | 49
Anemia | 87 | 33 | 82 | 27
Neutropenia | 76 | 33 | 76 | 33
Thrombocytopenia | 64 | 9 | 62 | 7
Chemistry
Hypomagnesemia | 61 | 4.2 | 63 | 3.7
Hyponatremia | 56 | 4.8 | 50 | 4.7
Increased AST | 50 | 1.7 | 44 | 2.3
Increased ALT | 49 | 3.1 | 46 | 1
Hypocalcemia | 45 | 5 | 43 | 5
Hypokalemia | 44 | 15 | 41 | 11
Increased creatinine | 44 | 7 | 46 | 6
Hypoalbuminemia | 38 | 2.4 | 37 | 2.3
Increased alkaline phosphatase | 38 | 0.3 | 35 | 0.3
Hyperkalemia | 21 | 2.0 | 16 | 1

Persistent, Recurrent, or Metastatic Cervical Cancer

The safety of intravenous pembrolizumab in combination with paclitaxel and cisplatin or paclitaxel and carboplatin, with or without bevacizumab, was investigated in KEYNOTE-826, a multicenter, double-blind, randomized (1:1), placebo-controlled trial in patients with persistent, recurrent, or first-line metastatic cervical cancer who had not been treated with chemotherapy except when used concurrently as a radio-sensitizing agent [see Clinical Studies (14.11)]. A total of 616 patients, regardless of tumor PD-L1 expression, received intravenous pembrolizumab 200 mg and chemotherapy with or without bevacizumab (n=307) every 3 weeks or placebo and chemotherapy with or without bevacizumab (n=309) every 3 weeks.

The median duration of exposure to intravenous pembrolizumab was 9.9 months (range: 1 day to 26 months).

Fatal adverse reactions occurred in 4.6% of patients receiving intravenous pembrolizumab in combination with chemotherapy with or without bevacizumab, including 3 cases of hemorrhage, 2 cases of sepsis, 2 cases due to unknown causes, and 1 case each of acute myocardial infarction, autoimmune encephalitis, cardiac arrest, cerebrovascular accident, femur fracture with perioperative pulmonary embolus, intestinal perforation, and pelvic infection.

Serious adverse reactions occurred in 50% of patients receiving intravenous pembrolizumab in combination with chemotherapy with or without bevacizumab. Serious adverse reactions in ≥3% of patients included febrile neutropenia (6.8%), urinary tract infection (5.2%), anemia (4.6%), acute kidney injury (3.3%), and sepsis (3.3%).

Intravenous pembrolizumab was discontinued for adverse reactions in 15% of patients. The most common adverse reaction resulting in permanent discontinuation of intravenous pembrolizumab (≥1%) was colitis (1%).

Adverse reactions leading to interruption of intravenous pembrolizumab occurred in 66% of patients; the most common adverse reactions or laboratory abnormalities leading to interruption of intravenous pembrolizumab (≥2%) were thrombocytopenia (15%), neutropenia (14%), anemia (11%), increased ALT (6%), leukopenia (5%), fatigue/asthenia (4.2%), urinary tract infection (3.6%), increased AST (3.3%), pyrexia (3.3%), diarrhea (2.6%), acute kidney injury (2.6%), increased blood creatinine (2.6%), colitis (2.3%), decreased appetite (2%), and cough (2%).

For patients treated with intravenous pembrolizumab, chemotherapy, and bevacizumab (n=196), the most common (≥20%) adverse reactions were peripheral neuropathy (62%), alopecia (58%), anemia (55%), fatigue/asthenia (53%), nausea (41%), neutropenia (41%), diarrhea (39%), hypertension (35%), thrombocytopenia (35%), constipation (31%), arthralgia (31%), vomiting (30%), urinary tract infection (27%), rash (26%), leukopenia (24%), hypothyroidism (22%), and decreased appetite (21%).

Table 39 and Table 40 summarize adverse reactions and laboratory abnormalities, respectively, in patients on intravenous pembrolizumab in KEYNOTE-826.

Table 39: Adverse Reactions Occurring in ≥20% of Patients Receiving Intravenous Pembrolizumab in KEYNOTE-826
Adverse Reaction | Intravenous Pembrolizumab 200 mg every 3 weeks and chemotherapy [Chemotherapy (paclitaxel and cisplatin or paclitaxel and carboplatin)] with or without bevacizumab n=307 |  | Placebo and chemotherapy with or without bevacizumab n=309
Adverse Reaction | All Grades [Graded per NCI CTCAE v4.0] (%) | Grades 3-4 (%) | All Grades (%) | Grades 3-4 (%)
Nervous System
Peripheral neuropathy [Includes neuropathy peripheral, peripheral sensory neuropathy, peripheral motor neuropathy, peripheral sensorimotor neuropathy, paresthesia] | 58 | 4.2 | 57 | 6
Skin and Subcutaneous Tissue
Alopecia | 56 | 0 | 58 | 0
Rash [Includes rash, rash maculo-papular, rash erythematous, rash macular, rash papular, rash pruritic, rash pustular] | 22 | 3.6 | 15 | 0.3
General
Fatigue [Includes fatigue, asthenia] | 47 | 7 | 46 | 6
Gastrointestinal
Nausea | 40 | 2 | 44 | 1.6
Diarrhea | 36 | 2 | 30 | 2.6
Constipation | 28 | 0.3 | 33 | 1
Vomiting | 26 | 2.6 | 27 | 1.9
Musculoskeletal and Connective Tissue
Arthralgia | 27 | 0.7 | 26 | 1.3
Vascular
Hypertension | 24 | 9 | 23 | 11
Infections
Urinary tract infection | 24 | 9 | 26 | 8

Table 40: Laboratory Abnormalities Worsened from Baseline Occurring in ≥20% of Patients Receiving Intravenous Pembrolizumab in KEYNOTE-826
Laboratory Test [Each test incidence is based on the number of patients who had both baseline and at least one on-study laboratory measurement available: intravenous pembrolizumab plus chemotherapy (range: 296 to 301 patients) and placebo plus chemotherapy (range: 299 to 302 patients)] | Intravenous Pembrolizumab 200 mg every 3 weeks and chemotherapy [Chemotherapy (paclitaxel and cisplatin or paclitaxel and carboplatin)] with or without bevacizumab n=307 |  | Placebo and chemotherapy with or without bevacizumab n=309
Laboratory Test [Each test incidence is based on the number of patients who had both baseline and at least one on-study laboratory measurement available: intravenous pembrolizumab plus chemotherapy (range: 296 to 301 patients) and placebo plus chemotherapy (range: 299 to 302 patients)] | All Grades [Graded per NCI CTCAE v4.0] (%) | Grades 3-4 (%) | All Grades (%) | Grades 3-4 (%)
Hematology
Anemia | 80 | 35 | 77 | 33
Leukopenia | 76 | 27 | 69 | 19
Neutropenia | 73 | 43 | 62 | 32
Lymphopenia | 64 | 35 | 59 | 35
Thrombocytopenia | 57 | 19 | 53 | 15
Chemistry
Hyperglycemia | 51 | 4.7 | 46 | 2.3
Hypoalbuminemia | 46 | 1.4 | 37 | 5
Hyponatremia | 39 | 14 | 38 | 11
Increased ALT | 40 | 7 | 38 | 6
Increased AST | 40 | 6 | 36 | 3.0
Increased alkaline phosphatase | 38 | 3.4 | 40 | 2.3
Hypocalcemia | 37 | 4.1 | 31 | 5
Increased creatinine | 34 | 5 | 32 | 6
Hypokalemia | 29 | 7 | 26 | 7
Hyperkalemia | 23 | 3.7 | 27 | 4.7
Hypercalcemia | 21 | 1.0 | 20 | 1.3

Previously Treated Recurrent or Metastatic Cervical Cancer

Among the 98 patients with cervical cancer enrolled in Cohort E of KEYNOTE-158 [see Clinical Studies (14.11)], the median duration of exposure to intravenous pembrolizumab was 2.9 months (range: 1 day to 22.1 months). Patients with autoimmune disease or a medical condition that required immunosuppression were ineligible.

Intravenous pembrolizumab was discontinued due to adverse reactions in 8% of patients. Serious adverse reactions occurred in 39% of patients receiving intravenous pembrolizumab. The most frequent serious adverse reactions reported included anemia (7%), fistula (4.1%), hemorrhage (4.1%), and infections [except UTIs] (4.1%). Tables 41 and 42 summarize adverse reactions and laboratory abnormalities, respectively, in patients on intravenous pembrolizumab in KEYNOTE-158.

Table 41: Adverse Reactions Occurring in ≥10% of Patients with Cervical Cancer in KEYNOTE-158
Adverse Reaction | Intravenous Pembrolizumab 200 mg every 3 weeks N=98
 | All Grades [Graded per NCI CTCAE v4.0] (%) | Grades 3–4 (%)
General
Fatigue [Includes asthenia, fatigue, lethargy, malaise] | 43 | 5
Pain [Includes breast pain, cancer pain, dysesthesia, dysuria, ear pain, gingival pain, groin pain, lymph node pain, oropharyngeal pain, pain, pain of skin, pelvic pain, radicular pain, stoma site pain, toothache] | 22 | 2.0
Pyrexia | 19 | 1.0
Edema peripheral [Includes edema peripheral, peripheral swelling] | 15 | 2.0
Musculoskeletal and Connective Tissue
Musculoskeletal pain [Includes arthralgia, back pain, musculoskeletal chest pain, musculoskeletal pain, myalgia, myositis, neck pain, non-cardiac chest pain, pain in extremity] | 27 | 5
Gastrointestinal
Diarrhea [Includes colitis, diarrhea, gastroenteritis] | 23 | 2.0
Abdominal pain [Includes abdominal discomfort, abdominal distension, abdominal pain, abdominal pain lower, abdominal pain upper] | 22 | 3.1
Nausea | 19 | 0
Vomiting | 19 | 1.0
Constipation | 14 | 0
Metabolism and Nutrition
Decreased appetite | 21 | 0
Vascular
Hemorrhage [Includes epistaxis, hematuria, hemoptysis, metrorrhagia, rectal hemorrhage, uterine hemorrhage, vaginal hemorrhage] | 19 | 5
Infections
UTI [Includes bacterial pyelonephritis, pyelonephritis acute, urinary tract infection, urinary tract infection bacterial, urinary tract infection pseudomonal, urosepsis] | 18 | 6
Infection (except UTI) [Includes cellulitis, clostridium difficile infection, device-related infection, empyema, erysipelas, herpes virus infection, infected neoplasm, infection, influenza, lower respiratory tract congestion, lung infection, oral candidiasis, oral fungal infection, osteomyelitis, pseudomonas infection, respiratory tract infection, tooth abscess, upper respiratory tract infection, uterine abscess, vulvovaginal candidiasis] | 16 | 4.1
Skin and Subcutaneous Tissue
Rash [Includes dermatitis, drug eruption, eczema, erythema, palmar-plantar erythrodysesthesia syndrome, rash, rash generalized, rash maculo-papular] | 17 | 2.0
Endocrine
Hypothyroidism | 11 | 0
Nervous System
Headache | 11 | 2.0
Respiratory, Thoracic and Mediastinal
Dyspnea | 10 | 1.0

Table 42: Laboratory Abnormalities Worsened from Baseline Occurring in ≥20% of Patients with Cervical Cancer in KEYNOTE-158
Laboratory Test [Each test incidence is based on the number of patients who had both baseline and at least one on-study laboratory measurement available: intravenous pembrolizumab (range: 76 to 79 patients)] | Intravenous Pembrolizumab 200 mg every 3 weeks
 | All Grades [Graded per NCI CTCAE v4.0] (%) | Grades 3-4 (%)
Hematology
Anemia | 54 | 24
Lymphopenia | 45 | 9
Chemistry
Hypoalbuminemia | 44 | 5
Increased alkaline phosphatase | 40 | 1.3
Hyponatremia | 38 | 13
Hyperglycemia | 38 | 1.3
Increased AST | 34 | 3.9
Increased creatinine | 32 | 5
Hypocalcemia | 27 | 0
Increased ALT | 21 | 3.9
Hypokalemia | 20 | 6

Other laboratory abnormalities occurring in ≥10% of patients receiving intravenous pembrolizumab were hypophosphatemia (19% all Grades; 6% Grades 3-4), increased INR (17% all Grades; 0% Grades 3-4), hypercalcemia (14% all Grades; 2.6% Grades 3-4), platelet count decreased (14% all Grades; 1.3% Grades 3-4), activated partial thromboplastin time prolonged (10% all Grades; 0% Grades 3-4), hypoglycemia (13% all Grades; 1.3% Grades 3-4), white blood cell decreased (13% all Grades; 2.6% Grades 3-4), and hyperkalemia (13% all Grades; 1.3% Grades 3-4).

HCC

Previously Treated HCC

The safety of intravenous pembrolizumab was investigated in KEYNOTE-394, a multicenter, double-blind, randomized, placebo-controlled trial that enrolled patients with previously treated HCC. Patients were randomized (2:1) and received intravenous pembrolizumab 200 mg (n=299) or placebo (n=153) intravenously every 3 weeks for up to 35 cycles [see Clinical Studies (14.12)].

The median duration of exposure was 3.3 months (range: 1 day to 27.3 months) in the intravenous pembrolizumab arm and 2.2 months (range: 1 day to 15.5 months) in the placebo arm. Intravenous pembrolizumab was discontinued due to adverse reactions in 13% of patients. The most common adverse reaction resulting in permanent discontinuation of intravenous pembrolizumab was ascites (2.3%). Adverse reactions leading to interruption of intravenous pembrolizumab occurred in 26% of patients; the most common adverse reactions or laboratory abnormalities leading to interruption of intravenous pembrolizumab (≥2%) were increased blood bilirubin (9%), increased AST (5%), and increased ALT (2%).

Tables 43 and 44 summarize adverse reactions and laboratory abnormalities, respectively, in patients on intravenous pembrolizumab in KEYNOTE-394.

Table 43: Adverse Reactions Occurring in ≥10% of Patients with HCC Receiving Intravenous Pembrolizumab in KEYNOTE-394
Adverse Reaction | Intravenous Pembrolizumab 200 mg every 3 weeks n=299 |  | Placebo n=153
Adverse Reaction | All Grades [Graded per NCI CTCAE v4.03] (%) | Grades 3-5 (%) | All Grades (%) | Grades 3-5 (%)
General
Pyrexia | 18 | 0.7 | 14 | 0
Skin and Subcutaneous Tissue
Rash [Includes dermatitis, dermatitis allergic, dermatitis bullous, rash, rash erythematous, rash maculo-papular, rash pustular, and blister.] | 18 | 0.7 | 7 | 0
Pruritus | 12 | 0 | 4 | 0
Gastrointestinal
Diarrhea | 16 | 1.7 | 9 | 0
Metabolism and Nutrition
Decreased appetite | 15 | 0.3 | 9 | 0
Infections
Upper respiratory tract infection | 11 | 1.0 | 7 | 0.7
Respiratory, Thoracic, and Mediastinal
Cough | 11 | 0 | 9 | 0
Endocrine
Hypothyroidism | 10 | 0 | 7 | 0

Table 44: Laboratory Abnormalities Worsened from Baseline Occurring in ≥20% of Patients with HCC Receiving Intravenous Pembrolizumab in KEYNOTE-394
Laboratory Test [Each test incidence is based on the number of patients who had both baseline and at least one on-study laboratory measurement available: intravenous pembrolizumab (range: 223 to 297 patients) and placebo (range: 144 to 151 patients).] | Intravenous Pembrolizumab |  | Placebo
Laboratory Test [Each test incidence is based on the number of patients who had both baseline and at least one on-study laboratory measurement available: intravenous pembrolizumab (range: 223 to 297 patients) and placebo (range: 144 to 151 patients).] | All Grades [Graded per NCI CTCAE v4.03] % | Grades 3-4 % | All Grades % | Grades 3-4 %
Chemistry
Increased AST | 54 | 14 | 44 | 12
Increased bilirubin | 47 | 11 | 36 | 7
Increased ALT | 47 | 7 | 32 | 4.6
Increased gamma-glutamyl transferase (GGT) | 40 | 20 | 39 | 15
Hypoalbuminemia | 40 | 0.7 | 20 | 0.7
Increased alkaline phosphatase | 39 | 4.1 | 34 | 4
Hyperglycemia | 36 | 3.3 | 26 | 1.4
Hyponatremia | 36 | 11 | 28 | 5
Hypophosphatemia | 30 | 6 | 17 | 4
Hypocalcemia | 24 | 1.4 | 15 | 0.7
Hematology
Lymphopenia | 44 | 11 | 34 | 4.6
Anemia | 36 | 7 | 30 | 3.3
Decreased platelets | 32 | 4.7 | 29 | 2
Leukopenia | 30 | 1.3 | 21 | 0.7
Neutropenia | 25 | 4.4 | 21 | 2

BTC

The safety of intravenous pembrolizumab in combination with gemcitabine and cisplatin, was investigated in KEYNOTE-966, a multicenter, double-blind, randomized, placebo-controlled trial in patients with locally advanced unresectable or metastatic BTC who had not received prior systemic therapy in the advanced disease setting [see Clinical Studies (14.13)]. A total of 1063 patients received either intravenous pembrolizumab 200 mg plus gemcitabine and cisplatin chemotherapy (n=529) or placebo plus gemcitabine and cisplatin chemotherapy (n=534) every 3 weeks.

The median duration of exposure to intravenous pembrolizumab was 6 months (range: 1 day to 28 months).

Intravenous pembrolizumab was discontinued for adverse reactions in 15% of patients. The most common adverse reaction resulting in permanent discontinuation of intravenous pembrolizumab (≥1%) was pneumonitis (1.3%).

Adverse reactions leading to the interruption of intravenous pembrolizumab occurred in 55% of patients. The most common adverse reactions or laboratory abnormalities leading to interruption of intravenous pembrolizumab (≥2%) were decreased neutrophil count (18%), decreased platelet count (10%), anemia (6%), decreased white blood count (4%), pyrexia (3.8%), fatigue (3.0%), cholangitis (2.8%), increased ALT (2.6%), increased AST (2.5%), and biliary obstruction (2.3%).

In the intravenous pembrolizumab plus chemotherapy versus placebo plus chemotherapy arms, there was a difference of ≥5% incidence in adverse reactions between patients treated with intravenous pembrolizumab versus placebo for pyrexia (26% vs 20%), rash (21% vs 13%), pruritus (15% vs 10%), and hypothyroidism (9% vs. 2.6%). There were no clinically meaningful differences in incidence of Grade 3-4 toxicity between arms.

There was a difference of ≥5% incidence in laboratory abnormalities between patients treated with intravenous pembrolizumab plus chemotherapy versus placebo plus chemotherapy for decreased lymphocytes (69% vs 61%). There were no clinically meaningful differences in incidence of Grade 3-4 toxicity between arms.

MCC

Among the 105 patients with MCC enrolled in KEYNOTE-017 and KEYNOTE-913 [see Clinical Studies (14.14)], the median duration of exposure to intravenous pembrolizumab was 6.3 months (range 1 day to 28 months). Patients with autoimmune disease or a medical condition that required immunosuppression were ineligible. Adverse reactions occurring in patients with MCC were similar to those occurring in 2799 patients with melanoma or NSCLC treated with intravenous pembrolizumab as a single agent. Laboratory abnormalities (Grades 3-4) that occurred at a higher incidence included increased lipase (17%).

RCC

In combination with axitinib in the first-line treatment of advanced RCC (KEYNOTE-426)

The safety of intravenous pembrolizumab in combination with axitinib was investigated in KEYNOTE-426 [see Clinical Studies (14.15)]. Patients with medical conditions that required systemic corticosteroids or other immunosuppressive medications or had a history of severe autoimmune disease other than type 1 diabetes, vitiligo, Sjogren's syndrome, and hypothyroidism stable on hormone replacement were ineligible. Patients received intravenous pembrolizumab 200 mg intravenously every 3 weeks and axitinib 5 mg orally twice daily, or sunitinib 50 mg once daily for 4 weeks and then off treatment for 2 weeks. The median duration of exposure to the combination therapy of intravenous pembrolizumab and axitinib was 10.4 months (range: 1 day to 21.2 months).

The study population characteristics were: median age of 62 years (range: 30 to 89), 40% age 65 or older; 71% male; 80% White; and 80% Karnofsky Performance Status (KPS) of 90-100 and 20% KPS of 70-80.

Fatal adverse reactions occurred in 3.3% of patients receiving intravenous pembrolizumab in combination with axitinib. These included 3 cases of cardiac arrest, 2 cases of pulmonary embolism and 1 case each of cardiac failure, death due to unknown cause, myasthenia gravis, myocarditis, Fournier's gangrene, plasma cell myeloma, pleural effusion, pneumonitis, and respiratory failure.

Serious adverse reactions occurred in 40% of patients receiving intravenous pembrolizumab in combination with axitinib. Serious adverse reactions in ≥1% of patients receiving intravenous pembrolizumab in combination with axitinib included hepatotoxicity (7%), diarrhea (4.2%), acute kidney injury (2.3%), dehydration (1%), and pneumonitis (1%).

Permanent discontinuation due to an adverse reaction of either intravenous pembrolizumab or axitinib occurred in 31% of patients; 13% intravenous pembrolizumab only, 13% axitinib only, and 8% both drugs. The most common adverse reaction (>1%) resulting in permanent discontinuation of intravenous pembrolizumab, axitinib, or the combination was hepatotoxicity (13%), diarrhea/colitis (1.9%), acute kidney injury (1.6%), and cerebrovascular accident (1.2%).

Dose interruptions or reductions due to an adverse reaction, excluding temporary interruptions of intravenous pembrolizumab infusions due to infusion-related reactions, occurred in 76% of patients receiving intravenous pembrolizumab in combination with axitinib. This includes interruption of intravenous pembrolizumab in 50% of patients. Axitinib was interrupted in 64% of patients and dose reduced in 22% of patients. The most common adverse reactions (>10%) resulting in interruption of intravenous pembrolizumab were hepatotoxicity (14%) and diarrhea (11%), and the most common adverse reactions (>10%) resulting in either interruption or reduction of axitinib were hepatotoxicity (21%), diarrhea (19%), and hypertension (18%).

The most common adverse reactions (≥20%) in patients receiving intravenous pembrolizumab and axitinib were diarrhea, fatigue/asthenia, hypertension, hypothyroidism, decreased appetite, hepatotoxicity, palmar-plantar erythrodysesthesia, nausea, stomatitis/mucosal inflammation, dysphonia, rash, cough, and constipation.

Twenty-seven percent (27%) of patients treated with intravenous pembrolizumab in combination with axitinib received an oral prednisone dose equivalent to ≥40 mg daily for an immune-mediated adverse reaction.

Tables 45 and 46 summarize the adverse reactions and laboratory abnormalities, respectively, that occurred in at least 20% of patients treated with intravenous pembrolizumab and axitinib in KEYNOTE-426.

Table 45: Adverse Reactions Occurring in ≥20% of Patients Receiving Intravenous Pembrolizumab with Axitinib in KEYNOTE-426
Adverse Reaction | Intravenous Pembrolizumab 200 mg every 3 weeks and Axitinib n=429 |  | Sunitinib n=425
Adverse Reaction | All Grades [Graded per NCI CTCAE v4.03] (%) | Grades 3-4 (%) | All Grades (%) | Grades 3-4 (%)
Gastrointestinal
Diarrhea [Includes diarrhea, colitis, enterocolitis, gastroenteritis, enteritis, enterocolitis hemorrhagic] | 56 | 11 | 45 | 5
Nausea | 28 | 0.9 | 32 | 0.9
Constipation | 21 | 0 | 15 | 0.2
General
Fatigue/Asthenia | 52 | 5 | 51 | 10
Vascular
Hypertension [Includes hypertension, blood pressure increased, hypertensive crisis, labile hypertension] | 48 | 24 | 48 | 20
Hepatobiliary
Hepatotoxicity [Includes ALT increased, AST increased, autoimmune hepatitis, blood bilirubin increased, drug-induced liver injury, hepatic enzyme increased, hepatic function abnormal, hepatitis, hepatitis fulminant, hepatocellular injury, hepatotoxicity, hyperbilirubinemia, immune-mediated hepatitis, liver function test increased, liver injury, transaminases increased] | 39 | 20 | 25 | 4.9
Endocrine
Hypothyroidism | 35 | 0.2 | 32 | 0.2
Metabolism and Nutrition
Decreased appetite | 30 | 2.8 | 29 | 0.7
Skin and Subcutaneous Tissue
Palmar-plantar erythrodysesthesia syndrome | 28 | 5 | 40 | 3.8
Stomatitis/Mucosal inflammation | 27 | 1.6 | 41 | 4
Rash [Includes rash, butterfly rash, dermatitis, dermatitis acneform, dermatitis atopic, dermatitis bullous, dermatitis contact, exfoliative rash, genital rash, rash erythematous, rash generalized, rash macular, rash maculopapular, rash papular, rash pruritic, seborrheic dermatitis, skin discoloration, skin exfoliation, perineal rash] | 25 | 1.4 | 21 | 0.7
Respiratory, Thoracic and Mediastinal
Dysphonia | 25 | 0.2 | 3.3 | 0
Cough | 21 | 0.2 | 14 | 0.5

Table 46: Laboratory Abnormalities Worsened from Baseline Occurring in ≥20% of Patients Receiving Intravenous Pembrolizumab with Axitinib in KEYNOTE-426
Laboratory Test [Each test incidence is based on the number of patients who had both baseline and at least one on-study laboratory measurement available: intravenous pembrolizumab/axitinib (range: 342 to 425 patients) and sunitinib (range: 345 to 421 patients).] | Intravenous Pembrolizumab 200 mg every 3 weeks and Axitinib |  | Sunitinib
Laboratory Test [Each test incidence is based on the number of patients who had both baseline and at least one on-study laboratory measurement available: intravenous pembrolizumab/axitinib (range: 342 to 425 patients) and sunitinib (range: 345 to 421 patients).] | All Grades [Graded per NCI CTCAE v4.03] % | Grades 3-4 % | All Grades % | Grades 3-4 %
Chemistry
Hyperglycemia | 62 | 9 | 54 | 3.2
Increased ALT | 60 | 20 | 44 | 5
Increased AST | 57 | 13 | 56 | 5
Increased creatinine | 43 | 4.3 | 40 | 2.4
Hyponatremia | 35 | 8 | 29 | 8
Hyperkalemia | 34 | 6 | 22 | 1.7
Hypoalbuminemia | 32 | 0.5 | 34 | 1.7
Hypercalcemia | 27 | 0.7 | 15 | 1.9
Hypophosphatemia | 26 | 6 | 49 | 17
Increased alkaline phosphatase | 26 | 1.7 | 30 | 2.7
Hypocalcemia [Corrected for albumin] | 22 | 0.2 | 29 | 0.7
Blood bilirubin increased | 22 | 2.1 | 21 | 1.9
Activated partial thromboplastin time prolonged [Two patients with a Grade 3 elevated activated partial thromboplastin time prolonged (aPTT) were also reported as having an adverse reaction of hepatotoxicity.] | 22 | 1.2 | 14 | 0
Hematology
Lymphopenia | 33 | 11 | 47 | 9
Anemia | 29 | 2.1 | 65 | 8
Thrombocytopenia | 27 | 1.4 | 78 | 14

In combination with lenvatinib in the first-line treatment of advanced RCC (KEYNOTE-581)

The safety of intravenous pembrolizumab was evaluated in KEYNOTE-581 [see Clinical Studies (14.15)]. Patients received intravenous pembrolizumab 200 mg intravenously every 3 weeks in combination with lenvatinib 20 mg orally once daily (n=352), or lenvatinib 18 mg orally once daily in combination with everolimus 5 mg orally once daily (n=355), or sunitinib 50 mg orally once daily for 4 weeks then off treatment for 2 weeks (n=340). The median duration of exposure to the combination therapy of intravenous pembrolizumab and lenvatinib was 17 months (range: 0.1 to 39).

Fatal adverse reactions occurred in 4.3% of patients treated with intravenous pembrolizumab in combination with lenvatinib, including cardio-respiratory arrest (0.9%), sepsis (0.9%), and one case (0.3%) each of arrhythmia, autoimmune hepatitis, dyspnea, hypertensive crisis, increased blood creatinine, multiple organ dysfunction syndrome, myasthenic syndrome, myocarditis, nephritis, pneumonitis, ruptured aneurysm, and subarachnoid hemorrhage.

Serious adverse reactions occurred in 51% of patients receiving intravenous pembrolizumab and lenvatinib. Serious adverse reactions in ≥2% of patients were hemorrhagic events (5%), diarrhea (4%), hypertension (3%), myocardial infarction (3%), pneumonitis (3%), vomiting (3%), acute kidney injury (2%), adrenal insufficiency (2%), dyspnea (2%), and pneumonia (2%).

Permanent discontinuation of either of intravenous pembrolizumab, lenvatinib or both due to an adverse reaction occurred in 37% of patients receiving intravenous pembrolizumab in combination with lenvatinib; 29% intravenous pembrolizumab only, 26% lenvatinib only, and 13% both. The most common adverse reactions (≥2%) resulting in permanent discontinuation of intravenous pembrolizumab, lenvatinib, or the combination were pneumonitis (3%), myocardial infarction (3%), hepatotoxicity (3%), acute kidney injury (3%), rash (3%), and diarrhea (2%).

Dose interruptions of intravenous pembrolizumab, lenvatinib, or both due to an adverse reaction occurred in 78% of patients receiving intravenous pembrolizumab in combination with lenvatinib. Intravenous pembrolizumab was interrupted in 55% of patients and both drugs were interrupted in 39% of patients. The most common adverse reactions (≥3%) resulting in interruption of intravenous pembrolizumab were diarrhea (10%), hepatotoxicity (8%), fatigue (7%), lipase increased (5%), amylase increased (4%), musculoskeletal pain (3%), hypertension (3%), rash (3%), acute kidney injury (3%), and decreased appetite (3%).

Fifteen percent (15%) of patients treated with intravenous pembrolizumab in combination with lenvatinib received an oral prednisone equivalent to ≥40 mg daily for an immune-mediated adverse reaction.

Tables 47 and 48 summarize the adverse reactions and laboratory abnormalities, respectively, that occurred in ≥20% of patients treated with intravenous pembrolizumab and lenvatinib in KEYNOTE-581.

Table 47: Adverse Reactions Occurring in ≥20% of Patients Receiving Intravenous Pembrolizumab with Lenvatinib in KEYNOTE-581
Adverse Reaction | Intravenous Pembrolizumab 200 mg every 3 weeks with Lenvatinib N=352 |  | Sunitinib 50 mg N=340
Adverse Reaction | All Grades (%) | Grades 3-4 (%) | All Grades (%) | Grades 3-4 (%)
General
Fatigue [Includes asthenia, fatigue, lethargy, malaise] | 63 | 9 | 56 | 8
Gastrointestinal
Diarrhea [Includes diarrhea, gastroenteritis] | 62 | 10 | 50 | 6
Stomatitis [Includes aphthous ulcer, gingival pain, glossitis, glossodynia, mouth ulceration, mucosal inflammation, oral discomfort, oral mucosal blistering, oral pain, oropharyngeal pain, pharyngeal inflammation, stomatitis] | 43 | 2 | 43 | 2
Nausea | 36 | 3 | 33 | 1
Abdominal pain [Includes abdominal discomfort, abdominal pain, abdominal rigidity, abdominal tenderness, epigastric discomfort, lower abdominal pain, upper abdominal pain] | 27 | 2 | 18 | 1
Vomiting | 26 | 3 | 20 | 1
Constipation | 25 | 1 | 19 | 0
Musculoskeletal and Connective Tissue
Musculoskeletal disorders [Includes arthralgia, arthritis, back pain, bone pain, breast pain, musculoskeletal chest pain, musculoskeletal discomfort, musculoskeletal pain, musculoskeletal stiffness, myalgia, neck pain, non-cardiac chest pain, pain in extremity, pain in jaw] | 58 | 4 | 41 | 3
Endocrine
Hypothyroidism [Includes hypothyroidism, increased blood thyroid stimulating hormone, secondary hypothyroidism] | 57 | 1 | 32 | 0
Vascular
Hypertension [Includes essential hypertension, increased blood pressure, increased diastolic blood pressure, hypertension, hypertensive crisis, hypertensive retinopathy, labile blood pressure] | 56 | 29 | 43 | 20
Hemorrhagic events [Includes all hemorrhage terms. Hemorrhage terms that occurred in 1 or more subjects in either treatment group include Anal hemorrhage, aneurysm ruptured, blood blister, blood loss anemia, blood urine present, catheter site hematoma, cerebral microhemorrhage, conjunctival hemorrhage, contusion, diarrhea hemorrhagic, disseminated intravascular coagulation, ecchymosis, epistaxis, eye hemorrhage, gastric hemorrhage, gastritis hemorrhagic, gingival bleeding, hemorrhage urinary tract, hemothorax, hematemesis, hematoma, hematochezia, hematuria, hemoptysis, hemorrhoidal hemorrhage, increased tendency to bruise, injection site hematoma, injection site hemorrhage, intra-abdominal hemorrhage, lower gastrointestinal hemorrhage, Mallory-Weiss syndrome, melaena, petechiae, rectal hemorrhage, renal hemorrhage, retroperitoneal hemorrhage, small intestinal hemorrhage, splinter hemorrhages, subcutaneous hematoma, subdural hematoma, subarachnoid hemorrhage, thrombotic thrombocytopenic purpura, tumor hemorrhage, traumatic hematoma, upper gastrointestinal hemorrhage] | 27 | 5 | 26 | 4
Metabolism
Decreased appetite [Includes decreased appetite, early satiety] | 41 | 4 | 31 | 1
Skin and Subcutaneous Tissue
Rash [Includes genital rash, infusion site rash, penile rash, perineal rash, rash, rash erythematous, rash macular, rash maculo-papular, rash papular, rash pruritic, rash pustular] | 37 | 5 | 17 | 1
Palmar-plantar erythrodysesthesia syndrome [Includes palmar erythema, palmar-plantar erythrodysesthesia syndrome, plantar erythema] | 29 | 4 | 38 | 4
Investigations
Weight loss | 30 | 8 | 9 | 0.3
Respiratory, Thoracic and Mediastinal
Dysphonia | 30 | 0 | 4 | 0
Renal and Urinary
Proteinuria [Includes hemoglobinuria, nephrotic syndrome, proteinuria] | 30 | 8 | 13 | 3
Acute kidney injury [Includes acute kidney injury, azotemia, blood creatinine increased, creatinine renal clearance decreased, hypercreatininemia, renal failure, renal impairment, oliguria, glomerular filtration rate decreased, and nephropathy toxic] | 21 | 5 | 16 | 2
Hepatobiliary
Hepatotoxicity [Includes alanine aminotransferase increased, aspartate aminotransferase increased, blood bilirubin increased, drug-induced liver injury, hepatic enzyme increased, hepatic failure, hepatic function abnormal, hepatocellular injury, hepatotoxicity, hyperbilirubinemia, hypertransaminasemia, immune-mediated hepatitis, liver function test increased, liver injury, transaminases increased, gamma-glutamyltransferase increased] | 25 | 9 | 21 | 5
Nervous System
Headache | 23 | 1 | 16 | 1

Clinically relevant adverse reactions (<20%) that occurred in patients receiving intravenous pembrolizumab with lenvatinib were myocardial infarction (3%) and angina pectoris (1%).

Table 48: Laboratory Abnormalities Worsened from Baseline Occurring in ≥20% (All Grades) of Patients Receiving Intravenous Pembrolizumab with Lenvatinib in KEYNOTE-581
Laboratory Test [With at least one Grade increase from baseline] | Intravenous Pembrolizumab 200 mg every 3 weeks with Lenvatinib |  | Sunitinib 50 mg
Laboratory Test [With at least one Grade increase from baseline] | All Grades % [Laboratory abnormality percentage is based on the number of patients who had both baseline and at least one post-baseline laboratory measurement for each parameter: intravenous pembrolizumab with lenvatinib (range: 343 to 349 patients) and sunitinib (range: 329 to 335 patients).] | Grade 3-4 % | All Grades % | Grade 3-4 %
Chemistry
Hypertriglyceridemia | 80 | 15 | 71 | 15
Hypercholesterolemia | 64 | 5 | 43 | 1
Increased lipase | 61 | 34 | 59 | 28
Increased creatinine | 61 | 5 | 61 | 2
Increased amylase | 59 | 17 | 41 | 9
Increased AST | 58 | 7 | 57 | 3
Hyperglycemia | 55 | 7 | 48 | 3
Increased ALT | 52 | 7 | 49 | 4
Hyperkalemia | 44 | 9 | 28 | 6
Hypoglycemia | 44 | 2 | 27 | 1
Hyponatremia | 41 | 12 | 28 | 9
Decreased albumin | 34 | 0.3 | 22 | 0
Increased alkaline phosphatase | 32 | 4 | 32 | 1
Hypocalcemia | 30 | 2 | 22 | 1
Hypophosphatemia | 29 | 7 | 50 | 8
Hypomagnesemia | 25 | 2 | 15 | 3
Increased creatine phosphokinase | 24 | 6 | 36 | 5
Hypermagnesemia | 23 | 2 | 22 | 3
Hypercalcemia | 21 | 1 | 11 | 1
Hematology
Lymphopenia | 54 | 9 | 66 | 15
Thrombocytopenia | 39 | 2 | 73 | 13
Anemia | 38 | 3 | 66 | 8
Leukopenia | 34 | 1 | 77 | 8
Neutropenia | 31 | 4 | 72 | 16

Grade 3 and 4 increased ALT or AST was seen in 9% of patients. Grade ≥2 increased ALT or AST was reported in 64 (18%) patients, of whom 20 (31%) received ≥40 mg daily oral prednisone equivalent. Recurrence of Grade ≥2 increased ALT or AST was observed on rechallenge in 10 patients receiving both intravenous pembrolizumab and lenvatinib (n=38) and was not observed on rechallenge with intravenous pembrolizumab alone (n=3).

Adjuvant treatment of RCC

The safety of intravenous pembrolizumab as a single agent was investigated in KEYNOTE-564, a randomized (1:1) double-blind placebo-controlled trial in which 984 patients who had undergone nephrectomy for RCC received 200 mg of intravenous pembrolizumab by intravenous infusion every 3 weeks (n=488) or placebo (n=496) for up to one year [see Clinical Studies (14.15)]. The median duration of exposure to intravenous pembrolizumab was 11.1 months (range: 1 day to 14.3 months). Patients with active autoimmune disease or a medical condition that required immunosuppression were ineligible.

Serious adverse reactions occurred in 20% of these patients receiving intravenous pembrolizumab. Serious adverse reactions (≥1%) were acute kidney injury, adrenal insufficiency, pneumonia, colitis, and diabetic ketoacidosis (1% each). Fatal adverse reactions occurred in 0.2% of those treated with intravenous pembrolizumab, including one case of pneumonia.

Discontinuation of intravenous pembrolizumab due to an adverse reaction occurred in 21% of patients; the most common (≥1%) were increased ALT (1.6%), colitis (1%), and adrenal insufficiency (1%).

Dose interruptions of intravenous pembrolizumab due to an adverse reaction occurred in 26% of patients; the most common (≥1%) were increased AST (2.3%), arthralgia (1.6%), hypothyroidism (1.6%), diarrhea (1.4%), increased ALT (1.4%), fatigue (1.4%), rash, decreased appetite, and vomiting (1% each).

Tables 49 and 50 summarize adverse reactions and laboratory abnormalities, respectively, in patients on intravenous pembrolizumab in KEYNOTE-564.

Table 49: Selected [Adverse reactions occurring at same or higher incidence than in placebo arm] Adverse Reactions Occurring in ≥10% of Patients Receiving Intravenous Pembrolizumab in KEYNOTE-564
Adverse Reaction | Intravenous Pembrolizumab 200 mg every 3 weeks n=488 |  | Placebo n=496
Adverse Reaction | All Grades [Graded per NCI CTCAE v4.0] (%) | Grades 3-4 (%) | All Grades (%) | Grades 3-4 (%)
Musculoskeletal and Connective Tissue
Musculoskeletal pain [Includes arthralgia, back pain, myalgia, arthritis, pain in extremity, neck pain, musculoskeletal pain, musculoskeletal stiffness, spinal pain, musculoskeletal chest pain, bone pain, musculoskeletal discomfort] | 41 | 1.2 | 36 | 0.6
General
Fatigue [Includes asthenia, fatigue] | 40 | 1.2 | 31 | 0.2
Skin and Subcutaneous Tissue
Rash [Includes rash, rash maculo-papular, rash papular, skin exfoliation, lichen planus, rash erythematous, eczema, rash macular, dermatitis acneiform, dermatitis, rash pruritic, Stevens-Johnson Syndrome, eczema asteatotic, palmar-plantar erythrodysesthesia syndrome] | 30 | 1.4 | 15 | 0.4
Pruritus | 23 | 0.2 | 13 | 0
Gastrointestinal
Diarrhea [Includes diarrhea, colitis, enterocolitis, frequent bowel movements, enteritis] | 27 | 2.7 | 23 | 0.2
Nausea | 16 | 0.4 | 10 | 0
Abdominal pain [Includes abdominal pain, abdominal pain lower, abdominal pain upper, abdominal discomfort, gastrointestinal pain] | 11 | 0.4 | 13 | 0.2
Endocrine
Hypothyroidism | 21 | 0.2 | 3.6 | 0
Hyperthyroidism | 12 | 0.2 | 0.2 | 0
Respiratory, Thoracic and Mediastinal
Cough [Includes upper-airway cough syndrome, productive cough, cough] | 17 | 0 | 12 | 0
Nervous System
Headache [Includes tension headache, headache, sinus headache, migraine with aura] | 15 | 0.2 | 13 | 0
Hepatobiliary
Hepatotoxicity [Includes alanine aminotransferase increased, aspartate aminotransferase increased, blood bilirubin increased, drug-induced liver injury, hepatic enzyme increased, hepatic function abnormal, hepatocellular injury, hepatotoxicity, hyperbilirubinemia, immune-mediated hepatitis, liver function test increased, transaminases increased, gamma-glutamyltransferase increased, bilirubin conjugated increased] | 14 | 3.7 | 7 | 0.6
Renal and Urinary
Acute kidney injury [Includes acute kidney injury, blood creatinine increased, renal failure, renal impairment, oliguria, glomerular filtration rate decreased, nephropathy toxic] | 13 | 1.2 | 10 | 0.2

Table 50: Selected [Laboratory abnormalities occurring at same or higher incidence than placebo] Laboratory Abnormalities Worsened from Baseline Occurring in ≥20% of Patients Receiving Intravenous Pembrolizumab in KEYNOTE-564
Laboratory Test [Each test incidence is based on the number of patients who had both baseline and at least one on-study laboratory measurement available: intravenous pembrolizumab (range: 440 to 449 patients) and placebo (range: 461 to 469 patients); increased INR: intravenous pembrolizumab n=199 and placebo n=224.] | Intravenous Pembrolizumab 200 mg every 3 weeks |  | Placebo
Laboratory Test [Each test incidence is based on the number of patients who had both baseline and at least one on-study laboratory measurement available: intravenous pembrolizumab (range: 440 to 449 patients) and placebo (range: 461 to 469 patients); increased INR: intravenous pembrolizumab n=199 and placebo n=224.] | All Grades [Graded per NCI CTCAE v4.03] % | Grades 3-4 % | All Grades % | Grades 3-4 %
Chemistry
Hyperglycemia | 48 | 8 | 45 | 4.5
Increased creatinine | 39 | 1.1 | 28 | 0.2
Increased INR | 29 | 1.0 | 20 | 0.9
Hyponatremia | 21 | 3.3 | 13 | 1.9
Increased ALT | 20 | 3.6 | 11 | 0.2
Hematology
Anemia | 28 | 0.5 | 20 | 0.4

Endometrial Carcinoma

Primary Advanced or Recurrent Endometrial Carcinoma

The safety of intravenous pembrolizumab in combination with chemotherapy (paclitaxel and carboplatin) was investigated in KEYNOTE-868, a randomized (1:1), multicenter, double-blind, placebo-controlled trial that enrolled patients with advanced or recurrent endometrial carcinoma [see Clinical Studies (14.16)]. A total of 759 patients received intravenous pembrolizumab 200 mg every 3 weeks and chemotherapy for 6 cycles followed by intravenous pembrolizumab 400 mg every 6 weeks for up to 14 cycles (n=382) or placebo and chemotherapy for 6 cycles followed by placebo for up to 14 cycles (n=377). The median duration of exposure to intravenous pembrolizumab was 5.6 months (range: 1 day to 24.0 months).

Serious adverse reactions occurred in 35% of patients receiving intravenous pembrolizumab in combination with chemotherapy, compared to 19% of patients receiving placebo in combination with chemotherapy.

Fatal adverse reactions occurred in 1.6% of patients receiving intravenous pembrolizumab in combination with chemotherapy, including COVID-19 (0.5%), and cardiac arrest (0.3%).

Intravenous pembrolizumab was discontinued for an adverse reaction in 14% of patients. Chemotherapy dose reduction was required in 29% of patients receiving intravenous pembrolizumab in combination with chemotherapy, compared to 23% of patients receiving placebo in combination with chemotherapy. There were no clinically meaningful differences in chemotherapy discontinuations or interruptions between arms.

Adverse reactions occurring in patients treated with intravenous pembrolizumab and chemotherapy were generally similar to those observed with intravenous pembrolizumab alone or chemotherapy alone with the exception of rash (33% all Grades; 2.9% Grades 3-4).

In Combination with Lenvatinib for the Treatment of Advanced Endometrial Carcinoma That Is pMMR or Not MSI-H.

The safety of intravenous pembrolizumab in combination with lenvatinib was investigated in KEYNOTE-775, a multicenter, open-label, randomized (1:1), active-controlled trial in patients with advanced endometrial carcinoma previously treated with at least one prior platinum-based chemotherapy regimen in any setting, including in the neoadjuvant and adjuvant settings [see Clinical Studies (14.16)]. Patients with endometrial carcinoma that is pMMR or not MSI-H received intravenous pembrolizumab 200 mg every 3 weeks in combination with lenvatinib 20mg orally once daily (n=342) or received doxorubicin or paclitaxel (n=325).

For patients with pMMR or not MSI-H tumor status, the median duration of study treatment was 7.2 months (range 1 day to 26.8 months) and the median duration of exposure to intravenous pembrolizumab was 6.8 months (range: 1 day to 25.8 months).

Fatal adverse reactions among these patients occurred in 4.7% of those treated with intravenous pembrolizumab and lenvatinib, including 2 cases of pneumonia, and 1 case of the following: acute kidney injury, acute myocardial infarction, colitis, decreased appetite, intestinal perforation, lower gastrointestinal hemorrhage, malignant gastrointestinal obstruction, multiple organ dysfunction syndrome, myelodysplastic syndrome, pulmonary embolism, and right ventricular dysfunction.

Serious adverse reactions occurred in 50% of these patients receiving intravenous pembrolizumab and lenvatinib. Serious adverse reactions (≥3%) were hypertension (4.4%) and urinary tract infections (3.2%).

Discontinuation of intravenous pembrolizumab due to an adverse reaction occurred in 15% of these patients. The most common adverse reaction leading to discontinuation of intravenous pembrolizumab (≥1%) was increased ALT (1.2%).

Dose interruptions of intravenous pembrolizumab due to an adverse reaction occurred in 48% of these patients. The most common adverse reactions leading to interruption of intravenous pembrolizumab (≥3%) were diarrhea (8%), increased ALT (4.4%), increased AST (3.8%), and hypertension (3.5%).

Tables 51 and 52 summarize adverse reactions and laboratory abnormalities, respectively, in patients on intravenous pembrolizumab in combination with lenvatinib in KEYNOTE-775.

Table 51: Adverse Reactions Occurring in ≥20% of Patients with Endometrial Carcinoma in KEYNOTE-775
 | Endometrial Carcinoma (pMMR or not MSI-H)
Adverse Reaction | Intravenous Pembrolizumab 200 mg every 3 weeks and Lenvatinib n=342 |  | Doxorubicin or Paclitaxel n=325
 | All Grades [Graded per NCI CTCAE v4.03] (%) | Grades 3-4 (%) | All Grades (%) | Grades 3-4 (%)
Endocrine
Hypothyroidism [Includes hypothyroidism, blood thyroid stimulating hormone increased, thyroiditis, secondary hypothyroidism] | 67 | 0.9 | 0.9 | 0
Vascular
Hypertension [Includes hypertension, blood pressure increased, secondary hypertension, blood pressure abnormal, hypertensive encephalopathy, blood pressure fluctuation] | 67 | 39 | 6 | 2.5
Hemorrhagic events [Includes epistaxis, vaginal hemorrhage, hematuria, gingival bleeding, metrorrhagia, rectal hemorrhage, contusion, hematochezia, cerebral hemorrhage, conjunctival hemorrhage, gastrointestinal hemorrhage, hemoptysis, hemorrhage urinary tract, lower gastrointestinal hemorrhage, mouth hemorrhage, petechiae, uterine hemorrhage, anal hemorrhage, blood blister, eye hemorrhage, hematoma, hemorrhage intracranial, hemorrhagic stroke, melena, stoma site hemorrhage, upper gastrointestinal hemorrhage, wound hemorrhage, blood urine present, ecchymosis, hematemesis, hemorrhage subcutaneous, hepatic hematoma, injection site bruising, intestinal hemorrhage, laryngeal hemorrhage, pulmonary hemorrhage, subdural hematoma, umbilical hemorrhage, vessel puncture site bruise] | 25 | 2.6 | 15 | 0.9
General
Fatigue [Includes fatigue, asthenia, malaise, lethargy] | 58 | 11 | 54 | 6
Gastrointestinal
Diarrhea [Includes diarrhea, gastroenteritis] | 55 | 8 | 20 | 2.8
Nausea | 49 | 2.9 | 47 | 1.5
Vomiting | 37 | 2.3 | 21 | 2.2
Stomatitis [Includes stomatitis, mucosal inflammation, oropharyngeal pain, aphthous ulcer, mouth ulceration, cheilitis, oral mucosal erythema, tongue ulceration] | 35 | 2.6 | 26 | 1.2
Abdominal pain [Includes abdominal pain, abdominal pain upper, abdominal pain lower, abdominal discomfort, gastrointestinal pain, abdominal tenderness, epigastric discomfort] | 34 | 2.6 | 21 | 1.2
Constipation | 27 | 0 | 25 | 0.6
Musculoskeletal and Connective Tissue
Musculoskeletal disorders [Includes arthralgia, myalgia, back pain, pain in extremity, bone pain, neck pain, musculoskeletal pain, arthritis, musculoskeletal chest pain, musculoskeletal stiffness, non-cardiac chest pain, pain in jaw] | 53 | 5 | 27 | 0.6
Metabolism
Decreased appetite [Includes decreased appetite, early satiety] | 44 | 7 | 21 | 0
Investigations
Weight loss | 34 | 10 | 6 | 0.3
Renal and Urinary
Proteinuria [Includes proteinuria, protein urine present, hemoglobinuria] | 29 | 6 | 3.4 | 0.3
Infections
Urinary tract infection [Includes urinary tract infection, cystitis, pyelonephritis] | 31 | 5 | 13 | 1.2
Nervous System
Headache | 26 | 0.6 | 9 | 0.3
Respiratory, Thoracic and Mediastinal
Dysphonia | 22 | 0 | 0.6 | 0
Skin and Subcutaneous Tissue
Palmar-plantar erythrodysesthesia [Includes palmar-plantar erythrodysesthesia syndrome, palmar erythema, plantar erythema] | 23 | 2.9 | 0.9 | 0
Rash [Includes rash, rash maculo-papular, rash pruritic, rash erythematous, rash macular, rash pustular, rash papular, rash vesicular, application site rash] | 20 | 2.3 | 4.9 | 0

Table 52: Laboratory Abnormalities Worsened from Baseline [With at least one grade increase from baseline] Occurring in ≥20% (All Grades) or ≥3% (Grades 3-4) of Patients with Endometrial Carcinoma in KEYNOTE-775
 | Endometrial Carcinoma (pMMR or not MSI-H)
Laboratory Test [Laboratory abnormality percentage is based on the number of patients who had both baseline and at least one post-baseline laboratory measurement for each parameter: intravenous pembrolizumab and lenvatinib (range: 263 to 340 patients) and doxorubicin or paclitaxel (range: 240 to 322 patients).] | Intravenous Pembrolizumab 200 mg every 3 weeks and Lenvatinib |  | Doxorubicin or Paclitaxel
 | All Grades [Graded per NCI CTCAE v4.03] % | Grades 3-4 % | All Grades % | Grades 3-4 %
Chemistry
Hypertriglyceridemia | 70 | 6 | 45 | 1.7
Hypoalbuminemia | 60 | 2.7 | 42 | 1.6
Increased aspartate aminotransferase | 58 | 9 | 23 | 1.6
Hyperglycemia | 58 | 8 | 45 | 4.4
Hypomagnesemia | 46 | 0 | 27 | 1.3
Increased alanine aminotransferase | 55 | 9 | 21 | 1.2
Hypercholesterolemia | 53 | 3.2 | 23 | 0.7
Hyponatremia | 46 | 15 | 28 | 7
Increased alkaline phosphatase | 43 | 4.7 | 18 | 0.9
Hypocalcemia | 40 | 4.7 | 21 | 1.9
Increased lipase | 36 | 14 | 13 | 3.9
Increased creatinine | 35 | 4.7 | 18 | 1.9
Hypokalemia | 34 | 10 | 24 | 5
Hypophosphatemia | 26 | 8 | 17 | 3.2
Increased amylase | 25 | 7 | 8 | 1
Hyperkalemia | 23 | 2.4 | 12 | 1.2
Increased creatine kinase | 19 | 3.7 | 7 | 0
Increased bilirubin | 18 | 3.6 | 6 | 1.6
Hematology
Lymphopenia | 51 | 18 | 66 | 23
Thrombocytopenia | 50 | 8 | 30 | 4.7
Anemia | 49 | 8 | 84 | 14
Leukopenia | 43 | 3.5 | 83 | 43
Neutropenia | 34 | 8 | 80 | 60

As a Single Agent for the Treatment of Advanced MSI-H or dMMR Endometrial Carcinoma

Among the 90 patients with MSI-H or dMMR endometrial carcinoma enrolled in KEYNOTE-158 [see Clinical Studies (14.16)] treated with intravenous pembrolizumab as a single agent, the median duration of exposure to intravenous pembrolizumab was 8.3 months (range: 1 day to 26.9 months). Adverse reactions occurring in patients with endometrial carcinoma were similar to those occurring in 2799 patients with melanoma or NSCLC treated with intravenous pembrolizumab as a single agent.

TMB-H Cancer

The safety of intravenous pembrolizumab was investigated in 105 patients with TMB-H cancer enrolled in KEYNOTE-158 [see Clinical Studies (14.17)]. The median duration of exposure to intravenous pembrolizumab was 4.9 months (range: 0.03 to 35.2 months). Adverse reactions occurring in patients with TMB-H cancer were similar to those occurring in patients with other solid tumors who received intravenous pembrolizumab as a single agent.

cSCC

Among the 159 patients with advanced cSCC (recurrent or metastatic or locally advanced disease) enrolled in KEYNOTE-629 [see Clinical Studies (14.18)], the median duration of exposure to intravenous pembrolizumab was 6.9 months (range 1 day to 28.9 months). Patients with autoimmune disease or a medical condition that required systemic corticosteroids or other immunosuppressive medications were ineligible. Adverse reactions occurring in patients with recurrent or metastatic cSCC or locally advanced cSCC were similar to those occurring in 2799 patients with melanoma or NSCLC treated with intravenous pembrolizumab as a single agent. Laboratory abnormalities (Grades 3-4) that occurred at a higher incidence included lymphopenia (10%) and decreased sodium (10%).

TNBC

Neoadjuvant and Adjuvant Treatment of High-Risk Early-Stage TNBC

The safety of intravenous pembrolizumab in combination with neoadjuvant chemotherapy (carboplatin and paclitaxel followed by doxorubicin or epirubicin and cyclophosphamide) followed by surgery and continued adjuvant treatment with intravenous pembrolizumab as a single agent was investigated in KEYNOTE-522, a randomized (2:1), multicenter, double-blind, placebo-controlled trial in patients with newly diagnosed, previously untreated, high-risk early-stage TNBC.

A total of 778 patients on the intravenous pembrolizumab arm received at least 1 dose of intravenous pembrolizumab in combination with neoadjuvant chemotherapy followed by intravenous pembrolizumab as adjuvant treatment after surgery, compared to 389 patients who received at least 1 dose of placebo in combination with neoadjuvant chemotherapy followed by placebo as adjuvant treatment after surgery [see Clinical Studies (14.19)].

The median duration of exposure to intravenous pembrolizumab 200 mg every 3 weeks was 13.3 months (range: 1 day to 21.9 months).

Fatal adverse reactions occurred in 0.9% of patients receiving intravenous pembrolizumab, including 1 each of adrenal crisis, autoimmune encephalitis, hepatitis, pneumonia, pneumonitis, pulmonary embolism, and sepsis in association with multiple organ dysfunction syndrome and myocardial infarction.

Serious adverse reactions occurred in 44% of patients receiving intravenous pembrolizumab. Serious adverse reactions in ≥2% of patients who received intravenous pembrolizumab included febrile neutropenia (15%), pyrexia (3.7%), anemia (2.6%), and neutropenia (2.2%).

Intravenous pembrolizumab was discontinued for adverse reactions in 20% of patients. The most common adverse reactions (≥1%) resulting in permanent discontinuation of intravenous pembrolizumab were increased ALT (2.7%), increased AST (1.5%), and rash (1%). Adverse reactions leading to the interruption of intravenous pembrolizumab occurred in 57% of patients. The most common adverse reactions leading to interruption of intravenous pembrolizumab (≥2%) were neutropenia (26%), thrombocytopenia (6%), increased ALT (6%), increased AST (3.7%), anemia (3.5%), rash (3.2%), febrile neutropenia (2.8%), leukopenia (2.8%), upper respiratory tract infection (2.6%), pyrexia (2.2%), and fatigue (2.1%).

Tables 53 and 54 summarize the adverse reactions and laboratory abnormalities, respectively, in patients treated with intravenous pembrolizumab in KEYNOTE-522.

Table 53: Adverse Reactions Occurring in ≥20% of Patients Receiving Intravenous Pembrolizumab in KEYNOTE-522
Adverse Reaction | Intravenous Pembrolizumab 200 mg every 3 weeks with chemotherapy [Chemotherapy: carboplatin and paclitaxel followed by doxorubicin or epirubicin and cyclophosphamide] / Intravenous Pembrolizumab n=778 |  | Placebo with chemotherapy/Placebo n=389
Adverse Reaction | All Grades [Graded per NCI CTCAE v4.0] (%) | Grades 3-4 (%) | All Grades (%) | Grades 3-4 (%)
General
Fatigue [Includes asthenia, fatigue] | 70 | 8 | 66 | 3.9
Pyrexia | 28 | 1.3 | 19 | 0.3
Gastrointestinal
Nausea | 67 | 3.7 | 66 | 1.8
Constipation | 42 | 0 | 39 | 0.3
Diarrhea | 41 | 3.2 | 34 | 1.8
Stomatitis [Includes aphthous ulcer, cheilitis, lip pain, lip ulceration, mouth ulceration, mucosal inflammation, oral mucosal eruption, oral pain, stomatitis, tongue blistering, tongue ulceration] | 34 | 2.7 | 29 | 1
Vomiting | 31 | 2.7 | 28 | 1.5
Abdominal pain [Includes abdominal discomfort, abdominal pain, abdominal pain lower, abdominal pain upper, abdominal tenderness] | 24 | 0.5 | 23 | 0.8
Skin and Subcutaneous Tissue
Alopecia | 61 | 0 | 58 | 0
Rash [Includes dermatitis, dermatitis acneiform, dermatitis allergic, dermatitis bullous, dermatitis exfoliative generalized, drug eruption, eczema, incision site rash, injection site rash, rash, rash erythematous, rash follicular, rash macular, rash maculo-papular, rash morbilliform, rash papular, rash pruritic, rash pustular, rash rubelliform, skin exfoliation, skin toxicity, toxic skin eruption, urticaria, vasculitic rash, viral rash] | 52 | 5 | 41 | 0.5
Nervous System
Peripheral neuropathy [Includes neuropathy peripheral, peripheral motor neuropathy, peripheral sensorimotor neuropathy, peripheral sensory neuropathy] | 41 | 3.3 | 42 | 2.3
Headache | 30 | 0.5 | 29 | 1
Musculoskeletal and Connective Tissue
Arthralgia | 29 | 0.5 | 31 | 0.3
Myalgia | 20 | 0.5 | 19 | 0
Respiratory, Thoracic and Mediastinal
Cough [Includes cough, productive cough, upper-airway cough syndrome] | 26 | 0.1 | 24 | 0
Metabolism and Nutrition
Decreased appetite | 23 | 0.9 | 17 | 0.3
Psychiatric
Insomnia | 21 | 0.5 | 19 | 0

Table 54: Laboratory Abnormalities Worsened from Baseline Occurring in ≥20% of Patients Receiving Intravenous Pembrolizumab in KEYNOTE-522
Laboratory Test [Each test incidence is based on the number of patients who had both baseline and at least one on-study laboratory measurement available: intravenous pembrolizumab in combination with chemotherapy followed by intravenous pembrolizumab as a single agent (range: 762 to 777 patients) and placebo in combination with chemotherapy followed by placebo (range: 381 to 389 patients).] | Intravenous Pembrolizumab 200 mg every 3 weeks with chemotherapy [Chemotherapy: carboplatin and paclitaxel followed by doxorubicin or epirubicin and cyclophosphamide] /Intravenous Pembrolizumab |  | Placebo with chemotherapy/Placebo
Laboratory Test [Each test incidence is based on the number of patients who had both baseline and at least one on-study laboratory measurement available: intravenous pembrolizumab in combination with chemotherapy followed by intravenous pembrolizumab as a single agent (range: 762 to 777 patients) and placebo in combination with chemotherapy followed by placebo (range: 381 to 389 patients).] | All Grades [Graded per NCI CTCAE v4.0] % | Grades 3-4 % | All Grades % | Grades 3-4 %
Hematology
Anemia | 97 | 22 | 96 | 19
Leukopenia | 93 | 41 | 91 | 32
Neutropenia | 88 | 62 | 89 | 62
Lymphopenia | 79 | 28 | 74 | 22
Thrombocytopenia | 57 | 10 | 56 | 8
Chemistry
Increased ALT | 70 | 9 | 67 | 3.9
Increased AST | 65 | 6 | 56 | 1.5
Hyperglycemia | 63 | 4.3 | 61 | 2.8
Increased alkaline phosphatase | 37 | 1 | 35 | 0.5
Hyponatremia | 35 | 9 | 25 | 4.6
Hypoalbuminemia | 34 | 1.0 | 30 | 1.3
Hypocalcemia | 31 | 2.2 | 28 | 3.1
Hypokalemia | 31 | 6 | 22 | 2.8
Hypophosphatemia | 20 | 6 | 15 | 4.2

Locally Recurrent Unresectable or Metastatic TNBC

The safety of intravenous pembrolizumab in combination with paclitaxel, paclitaxel protein-bound, or gemcitabine and carboplatin was investigated in KEYNOTE-355, a multicenter, double-blind, randomized (2:1), placebo-controlled trial in patients with locally recurrent unresectable or metastatic TNBC who had not been previously treated with chemotherapy in the metastatic setting [see Clinical Studies (14.19)]. A total of 596 patients (including 34 patients from a safety run-in) received intravenous pembrolizumab 200 mg every 3 weeks in combination with paclitaxel, paclitaxel protein-bound, or gemcitabine and carboplatin.

The median duration of exposure to intravenous pembrolizumab was 5.7 months (range: 1 day to 33.0 months).

Fatal adverse reactions occurred in 2.5% of patients receiving intravenous pembrolizumab in combination with chemotherapy, including cardio-respiratory arrest (0.7%) and septic shock (0.3%).

Serious adverse reactions occurred in 30% of patients receiving intravenous pembrolizumab in combination with paclitaxel, paclitaxel protein-bound, or gemcitabine and carboplatin. Serious adverse reactions in ≥2% of patients were pneumonia (2.9%), anemia (2.2%), and thrombocytopenia (2%).

Intravenous pembrolizumab was discontinued for adverse reactions in 11% of patients. The most common adverse reactions resulting in permanent discontinuation of intravenous pembrolizumab (≥1%) were increased ALT (2.2%), increased AST (1.5%), and pneumonitis (1.2%). Adverse reactions leading to the interruption of intravenous pembrolizumab occurred in 50% of patients. The most common adverse reactions leading to interruption of intravenous pembrolizumab (≥2%) were neutropenia (22%), thrombocytopenia (14%), anemia (7%), increased ALT (6%), leukopenia (5%), increased AST (5%), decreased white blood cell count (3.9%), and diarrhea (2%).

Tables 55 and 56 summarize the adverse reactions and laboratory abnormalities in patients on intravenous pembrolizumab in KEYNOTE-355.

Table 55: Adverse Reactions Occurring in ≥20% of Patients Receiving Intravenous Pembrolizumab with Chemotherapy in KEYNOTE-355
Adverse Reaction | Intravenous Pembrolizumab 200 mg every 3 weeks with chemotherapy n=596 |  | Placebo every 3 weeks with chemotherapy n=281
Adverse Reaction | All Grades [Graded per NCI CTCAE v4.03] (%) | Grades 3-4 (%) | All Grades (%) | Grades 3-4 (%)
General
Fatigue [Includes fatigue and asthenia] | 48 | 5 | 49 | 4.3
Gastrointestinal
Nausea | 44 | 1.7 | 47 | 1.8
Diarrhea | 28 | 1.8 | 23 | 1.8
Constipation | 28 | 0.5 | 27 | 0.4
Vomiting | 26 | 2.7 | 22 | 3.2
Skin and Subcutaneous Tissue
Alopecia | 34 | 0.8 | 35 | 1.1
Rash [Includes rash, rash maculo-papular, rash pruritic, rash pustular, rash macular, rash papular, butterfly rash, rash erythematous, eyelid rash] | 26 | 2 | 16 | 0
Respiratory, Thoracic and Mediastinal
Cough [Includes cough, productive cough, upper-airway cough syndrome] | 23 | 0 | 20 | 0.4
Metabolism and Nutrition
Decreased appetite | 21 | 0.8 | 14 | 0.4
Nervous System
Headache [Includes headache, migraine, tension headache] | 20 | 0.7 | 23 | 0.7

Table 56: Laboratory Abnormalities Worsened from Baseline Occurring in ≥20% of Patients Receiving Intravenous Pembrolizumab with Chemotherapy in KEYNOTE-355
Laboratory Test [Each test incidence is based on the number of patients who had both baseline and at least one on-study laboratory measurement available: intravenous pembrolizumab + chemotherapy (range: 566 to 592 patients) and placebo + chemotherapy (range: 269 to 280 patients).] | Intravenous Pembrolizumab 200 mg every 3 weeks with chemotherapy |  | Placebo every 3 weeks with chemotherapy
Laboratory Test [Each test incidence is based on the number of patients who had both baseline and at least one on-study laboratory measurement available: intravenous pembrolizumab + chemotherapy (range: 566 to 592 patients) and placebo + chemotherapy (range: 269 to 280 patients).] | All Grades [Graded per NCI CTCAE v4.03] % | Grades 3-4 % | All Grades % | Grades 3-4 %
Hematology
Anemia | 90 | 20 | 85 | 19
Leukopenia | 85 | 39 | 86 | 39
Neutropenia | 78 | 50 | 79 | 53
Lymphopenia | 73 | 28 | 71 | 19
Thrombocytopenia | 54 | 19 | 53 | 21
Chemistry
Increased ALT | 60 | 11 | 58 | 8
Increased AST | 57 | 9 | 55 | 6
Hyperglycemia | 52 | 4.4 | 51 | 2.2
Hypoalbuminemia | 36 | 2.0 | 32 | 2.2
Increased alkaline phosphatase | 35 | 3.9 | 39 | 2.2
Hypocalcemia | 29 | 3.3 | 27 | 1.8
Hyponatremia | 28 | 5 | 26 | 6
Hypophosphatemia | 21 | 7 | 18 | 4.8
Hypokalemia | 20 | 4.4 | 18 | 4.0

Ovarian Cancer

The safety of intravenous pembrolizumab in combination with paclitaxel with or without bevacizumab was evaluated in 463 patients with epithelial ovarian, fallopian tube, or primary peritoneal carcinoma whose tumors express PD-L1 (CPS ≥1) enrolled in KEYNOTE-B96 [see Clinical Studies (14.20)]. Among patients who received intravenous pembrolizumab, the median duration of exposure was 7.4 months (range: 1 day to 35.9 months).

Serious adverse reactions occurred in 54% of patients receiving intravenous pembrolizumab and paclitaxel with or without bevacizumab. Serious adverse reactions in ≥2% of patients were pneumonia (4.3%), urinary tract infection (3.9%), adrenal insufficiency (3%), hyponatremia (3%), COVID-19 (2.6%), decreased neutrophil count (2.6%), pulmonary embolism (2.6%), abdominal pain (2.1%), anemia (2.1%), colitis (2.1%), diarrhea (2.1%), febrile neutropenia (2.1%), pyrexia (2.1%) and vomiting (2.1%).

Fatal adverse reactions occurred in 3.9% of patients receiving intravenous pembrolizumab and paclitaxel with or without bevacizumab, including assisted suicide (0.9%), death (0.4%), intestinal perforation (0.4%), sepsis (0.4%), COVID-19 (0.4%), cardio-respiratory arrest (0.4%), colitis (0.4%), and embolic stroke (0.4%).

Intravenous pembrolizumab was permanently discontinued for adverse reactions in 16% of patients. The most common adverse reactions resulting in permanent discontinuation of intravenous pembrolizumab (≥1%) were colitis (1.3%) and increased alanine aminotransferase (1.3%). Adverse reactions leading to the interruption of intravenous pembrolizumab occurred in 44% of patients. The most common adverse reactions leading to interruption of intravenous pembrolizumab in ≥2% were urinary tract infection (3.9%), adrenal insufficiency (2.6%), pyrexia (2.6%), pneumonitis (2.6%), upper respiratory tract infection (2.6%), neutropenia (2.1%), diarrhea (2.1%) and COVID-19 (2.1%).

The most common (≥20%) adverse reactions for patients treated with intravenous pembrolizumab in combination with paclitaxel with or without bevacizumab were: diarrhea (45%), fatigue (43%), nausea (41%), alopecia (38%), peripheral neuropathy (38%), epistaxis (31%), urinary tract infection (27%), constipation (25%), abdominal pain (24%), decreased appetite (24%), vomiting (24%), hypothyroidism (21%), cough (20%), hypertension (20%), and rash (20%). The most common (≥20%) laboratory abnormalities worsening from baseline were: anemia (85%), leukopenia (82%), decreased neutrophil count (71%), lymphopenia (60%), hypoalbuminemia (50%), hyponatremia (53%), hypomagnesemia (45%), increased aspartate aminotransferase (43%), increased alanine aminotransferase (40%), hypocalcemia(40%), increased alkaline phosphatase (31%), increased creatinine (29%), hypokalemia (27%) and neutropenia (21%).

For patients treated with intravenous pembrolizumab in combination with paclitaxel and bevacizumab (N=169), decreased white blood cell count (27%), stomatitis (22%) and pyrexia (21%) were also reported as adverse reactions.

6.2 Postmarketing Experience

The following adverse reactions have been identified during post-approval use of intravenous pembrolizumab. Because these reactions are reported voluntarily from a population of uncertain size, it is not always possible to reliably estimate their frequency or establish a causal relationship to drug exposure.

Gastrointestinal: Exocrine pancreatic insufficiency

Hepatobiliary: sclerosing cholangitis

8 USE IN SPECIFIC POPULATIONS

8.1 Pregnancy

Risk Summary

Based on its mechanism of action [see Clinical Pharmacology (12.1)], KEYTRUDA QLEX can cause fetal harm when administered to a pregnant woman. There are no available human data informing the risk of embryo-fetal toxicity. In animal models, the PD-1/PD-L1 signaling pathway is important in the maintenance of pregnancy through induction of maternal immune tolerance to fetal tissue (see Data). Human IgG4 (immunoglobulins) are known to cross the placenta; therefore, pembrolizumab has the potential to be transmitted from the mother to the developing fetus. Advise pregnant women of the potential risk to a fetus.

In the U.S. general population, the estimated background risk of major birth defects and miscarriage in clinically recognized pregnancies is 2 to 4% and 15 to 20%, respectively.

Data

Animal Data

KEYTRUDA QLEX for subcutaneous injection contains pembrolizumab and berahyaluronidase alfa [see Description (11)].

Pembrolizumab:

Animal reproduction studies have not been conducted with pembrolizumab to evaluate its effect on reproduction and fetal development. A literature-based assessment of the effects of the PD-1 pathway on reproduction demonstrated that a central function of the PD-1/PD-L1 pathway is to preserve pregnancy by maintaining maternal immune tolerance to the fetus. Blockade of PD-L1 signaling has been shown in murine models of pregnancy to disrupt tolerance to the fetus and to result in an increase in fetal loss; therefore, potential risks of administering pembrolizumab during pregnancy include increased rates of abortion or stillbirth. As reported in the literature, there were no malformations related to the blockade of PD-1 signaling in the offspring of these animals; however, immune-mediated disorders occurred in PD-1 knockout mice. Based on its mechanism of action, fetal exposure to pembrolizumab may increase the risk of developing immune-mediated disorders or of altering the normal immune response.

Berahyaluronidase alfa:

In an embryo-fetal development study, pregnant rabbits were administered daily subcutaneous injections of 138,600, 403,200, or 1,209,600 U/kg berahyaluronidase alfa during the period of organogenesis (gestation days 6 to 19). Berahyaluronidase alfa caused delayed fetal development at doses ≥403,200 U/kg, which is >2,500 times higher than the human dose (U/kg basis). Increased post-implantation loss and visceral malformations (supernumerary fissure lung lobe) were observed at 1,209,600 U/kg, which is >7,500 times higher than the human dose. In an embryo-fetal development study in rats, there were no adverse embryo-fetal findings in pregnant animals administered daily subcutaneous injections of berahyaluronidase alfa at doses up to 2,520,000 U/kg (>15,000 times higher than the human dose) during the period of organogenesis (gestation days 6 to 17).

In a pre- and post-natal development study in rats, pregnant animals were administered daily subcutaneous injections of 280,000, 840,000, or 2,520,000 U/kg berahyaluronidase alfa from implantation through lactation and weaning (gestation day 6 to lactation day 21). There were no adverse effects on sexual maturation, learning and memory, or fertility of the offspring at doses up to 2,520,000 U/kg, which is >15,000 times higher than the human dose.

8.2 Lactation

Risk Summary

There are no data on the presence of pembrolizumab or berahyaluronidase alfa in either animal or human milk or its effects on the breastfed child or on milk production. Maternal IgG is known to be present in human milk.

The effects of local gastrointestinal exposure and limited systemic exposure in the breastfed child to KEYTRUDA QLEX are unknown. Because of the potential for serious adverse reactions in breastfed children, advise women not to breastfeed during treatment with KEYTRUDA QLEX and for 4 months after the last dose.

8.3 Females and Males of Reproductive Potential

Based on its mechanism of action, KEYTRUDA QLEX can cause fetal harm when administered to a pregnant woman [see Use in Specific Populations (8.1)].

Pregnancy Testing

Verify pregnancy status in females of reproductive potential prior to initiating KEYTRUDA QLEX [see Use in Specific Populations (8.1)].

Contraception

Advise females of reproductive potential to use effective contraception during treatment with KEYTRUDA QLEX and for 4 months after the last dose.

8.4 Pediatric Use

The safety and effectiveness of KEYTRUDA QLEX for the treatment of pediatric patients 12 years and older who weigh greater than 40 kg have been established for:

- Stage IIB, IIC, or III melanoma following complete resection [see Indications and Usage (1.1)]
- Unresectable or metastatic microsatellite instability high (MSI-H) or mismatch repair deficient (dMMR) solid tumors [see Indications and Usage (1.6)]
- Recurrent locally advanced or metastatic Merkel cell carcinoma [see Indications and Usage (1.13)]
- Unresectable or metastatic tumor mutational burden high solid tumors (TMB-H) [see Indications and Usage (1.16)]

Use of KEYTRUDA QLEX in pediatric patients for these indications is supported by evidence from adequate and well-controlled studies of intravenous pembrolizumab in adults and additional pharmacokinetic and safety data for intravenous pembrolizumab in pediatric patients 12 years and older [see Adverse Reactions (6.1), Clinical Studies (14)]. Pembrolizumab exposures in pediatric patients 12 years and older who weigh greater than 40 kg are predicted to be within range of those observed in adults at the same dosage [see Clinical Pharmacology (12.3)].

The safety and effectiveness of KEYTRUDA QLEX have not been established in pediatric patients younger than 12 years of age for the treatment of melanoma, MCC, MSI-H or dMMR cancer, and TMB-H cancer.

The safety and effectiveness of KEYTRUDA QLEX have not been established in pediatric patients for other approved indications [see Indications and Usage (1)].

Intravenous pembrolizumab

In KEYNOTE-051, 173 pediatric patients (including 108 pediatric patients aged 12 to 17 years) with advanced melanoma, lymphoma, or PD-L1 positive or MSI-H solid tumors received intravenous pembrolizumab 2 mg/kg every 3 weeks. The median duration of exposure was 2.1 months (range: 1 day to 25 months). Adverse reactions that occurred at a ≥10% higher rate in pediatric patients when compared to adults included pyrexia (33%), vomiting (29%), headache (25%), abdominal pain (23%), decreased lymphocyte count (13%), and decreased white blood cell count (11%). Laboratory abnormalities that occurred at a ≥10% higher rate in pediatric patients when compared to adults were leukopenia (30%), neutropenia (28%), thrombocytopenia (22%), and Grade 3 anemia (17%).

8.5 Geriatric Use

Of the 251 patients treated with KEYTRUDA QLEX in combination with platinum doublet chemotherapy in Study MK-3745A-D77, 53% were 65 years and older and 16% were 75 years and older. No overall differences in safety or effectiveness of KEYTRUDA QLEX have been observed between patients aged 65 years or older and younger adult patients.

The safety of KEYTRUDA QLEX as monotherapy or in combination with other antineoplastic drugs for its approved indications [see Indications and Usage (1)] has been established in adequate and well-controlled studies of intravenous pembrolizumab as a single agent and in combination with other antineoplastic drugs. Below is a description of geriatric use information from the intravenous pembrolizumab studies.

- Of 3781 patients with melanoma, NSCLC, HNSCC, or urothelial carcinoma who were treated with intravenous pembrolizumab in clinical studies, 48% were 65 years and over and 17% were 75 years and over.
- Of 506 adult patients with Stage IB (T2a ≥4 cm), II, or IIIA NSCLC following complete resection and platinum-based chemotherapy who were treated with intravenous pembrolizumab in KEYNOTE-091, 242 (48%) were 65 years and over.
- Of 596 adult patients with TNBC who were treated with intravenous pembrolizumab in combination with paclitaxel, paclitaxel protein-bound, or gemcitabine and carboplatin in KEYNOTE-355, 137 (23%) were 65 years and over.
- Of 406 adult patients with endometrial carcinoma who were treated with intravenous pembrolizumab in combination with lenvatinib in KEYNOTE-775, 201 (50%) were 65 years and over.
- Of the 564 patients with locally advanced or metastatic urothelial cancer treated with intravenous pembrolizumab in combination with enfortumab vedotin, 44% (n=247) were 65-74 years and 26% (n=144) were 75 years or older. No overall differences in effectiveness were observed between patients 65 years of age or older and younger patients. Patients 75 years of age or older treated with intravenous pembrolizumab in combination with enfortumab vedotin experienced a higher incidence of fatal adverse reactions than younger patients. The incidence of fatal adverse reactions was 4% in patients younger than 75 and 7% in patients 75 years or older.
- Of the 167 patients with MIBC treated with intravenous pembrolizumab in combination with enfortumab vedotin, 37% (n=61) were 65-74 years and 46% (n=77) were 75 years or older. Patients 75 years of age or older treated with intravenous pembrolizumab in combination with enfortumab vedotin experienced a higher incidence of fatal adverse reactions than younger patients. The incidence of fatal adverse reactions was 4% in patients younger than 75 and 12% in patients 75 years or older.
- Of the 432 patients randomized to intravenous pembrolizumab in combination with axitinib in the KEYNOTE-426 trial, 40% were 65 years or older.
- Of 294 adult patients with FIGO 2014 Stage III-IVA cervical cancer who were treated with intravenous pembrolizumab in combination with CRT in KEYNOTE-A18, 42 (14%) were 65 years and over.
- Of 643 adult patients with ovarian cancer who were treated with intravenous pembrolizumab in combination with paclitaxel with or without bevacizumab in KEYNOTE-B96, 236 (37%) were 65 years and over and 58 (9%) were 75 years and over.

No overall differences in safety or effectiveness were observed between intravenous pembrolizumab-treated patients aged 65 years or older and younger adult patients.

11 DESCRIPTION

KEYTRUDA QLEX is a fixed-combination drug product containing pembrolizumab and berahyaluronidase alfa.

Pembrolizumab is a programmed death receptor-1 (PD 1)-blocking antibody. Pembrolizumab is a humanized monoclonal IgG4 kappa antibody with an approximate molecular weight of 149 kDa. Pembrolizumab is produced in recombinant Chinese hamster ovary (CHO) cells.

Berahyaluronidase alfa is an endoglycosidase used to enhance dispersion and permeation, which facilitates delivery of increased volume of pembrolizumab that is co-administered subcutaneously. It is produced by mammalian CHO (Chinese Hamster Ovary) cells containing a DNA plasmid encoding a variant of human hyaluronidase PH20. It is a glycosylated protein with an approximate molecular weight of 49 kDa under nonreducing, deglycosylated conditions.

KEYTRUDA QLEX (pembrolizumab and berahyaluronidase alfa-pmph) injection is a sterile, preservative-free, clear to slightly opalescent, colorless to slightly yellow solution supplied in single-dose vials for subcutaneous administration.

KEYTRUDA QLEX is supplied as two different configurations:

- Each KEYTRUDA QLEX 2.4 mL single-dose vial contains 395 mg of pembrolizumab and 4,800 units of berahyaluronidase alfa, and histidine (0.7 mg), histidine hydrochloride monohydrate (4.1 mg), methionine (3.6 mg), polysorbate 80 (0.5 mg), sucrose (168 mg), and Water for Injection, USP. The pH is 5.3-5.9.
- Each KEYTRUDA QLEX 4.8 mL single-dose vial contains 790 mg of pembrolizumab and 9,600 units of berahyaluronidase alfa, and histidine (1.4 mg), histidine hydrochloride monohydrate (8.2 mg), methionine (7.2 mg), polysorbate 80 (1 mg), sucrose (336 mg), and Water for Injection, USP. The pH is 5.3-5.9.

12 CLINICAL PHARMACOLOGY

12.1 Mechanism of Action

Binding of the PD-1 ligands, PD-L1 and PD-L2, to the PD-1 receptor found on T cells, inhibits T cell proliferation and cytokine production. Upregulation of PD-1 ligands occurs in some tumors and signaling through this pathway can contribute to inhibition of active T-cell immune surveillance of tumors. Pembrolizumab is a monoclonal antibody that binds to the PD-1 receptor and blocks its interaction with PD-L1 and PD-L2, releasing PD-1 pathway-mediated inhibition of the immune response, including the anti-tumor immune response. In syngeneic mouse tumor models, blocking PD-1 activity resulted in decreased tumor growth.

In syngeneic mouse tumor models, combination treatment of a PD-1 blocking antibody and kinase inhibitor lenvatinib decreased tumor-associated macrophages, increased activated cytotoxic T cells, and reduced tumor growth compared to either treatment alone.

Berahyaluronidase alfa, an endoglycosidase, is a variant of human hyaluronidase PH20 that temporarily and locally breaks down hyaluronan. Hyaluronan is a polysaccharide found in the extracellular matrix of the subcutaneous tissue. Unlike the stable structural components of the interstitial matrix, hyaluronan has a half-life of approximately 0.5 days. Hyaluronidase increases permeability of the subcutaneous tissue by depolymerizing hyaluronan.

In the doses administered, the effects of berahyaluronidase alfa are reversible and permeability of the subcutaneous tissue is restored within 24 to 48 hours.

12.2 Pharmacodynamics

There are no clinically significant exposure-response relationships for efficacy or safety for intravenous pembrolizumab across the approved dosing regimens, regardless of cancer type. The exposures from subcutaneous KEYTRUDA QLEX doses of 395 mg/4,800 units every 3 weeks or 790 mg/9,600 units every 6 weeks are within the range of exposures from intravenous pembrolizumab doses.

12.3 Pharmacokinetics

Pembrolizumab pharmacokinetics were characterized at Cycle 1 and at steady state in patients with advanced solid tumors at the approved recommended dosages and are presented as mean (CV%) unless otherwise specified.

When comparing pembrolizumab exposure following subcutaneous administration every 6 weeks to that of intravenous administration every 6 weeks in Study MK-3475A-D77 [see Clinical Studies (14.1)], the geometric mean ratio (GMR) for Cycle 1 AUC0-6wks was 1.14 (96% CI: 1.06, 1.22) and Cycle 3 Ctrough (i.e., steady state) was 1.67 (94% CI: 1.52, 1.84).

Pembrolizumab steady state was reached by 16 weeks. At steady state following subcutaneous administration, the mean pembrolizumab AUC0-6wks was 2,798 mcg•day/mL for the every 6 week dosing and pembrolizumab AUC0-3wks was 1,343 mcg•day/mL for the every 3 week dosing. Pembrolizumab Ctrough was 39 mcg/mL for the every 6 week dosing and 49 mcg/mL for the every 3 week dosing.

The systemic accumulation ratio was 1.6-fold following administration of KEYTRUDA QLEX 790 mg/9,600 units every 6 weeks and 2.5-fold following administration of KEYTRUDA QLEX 395 mg/4,800 units every 3 weeks.

Absorption

Pembrolizumab bioavailability (CV%) is approximately 60% (14%). Peak concentrations occurred by approximately 4 days.

Distribution

The volume of distribution is 6 L.

Elimination

Pembrolizumab clearance decreases over time, resulting in a steady state clearance (CV%) of - 195 mL/day (40%); this decrease in clearance with time is not considered clinically significant. The terminal half-life is 22 days.

Specific Populations

No clinically significant differences in the pharmacokinetics of pembrolizumab were observed based on age (37 to 87 years), race (63% White, 28% Asian, 3% Black), sex, body weight (37 to 144 kg), tumor type, injection site (thigh or abdomen), estimated glomerular filtration rate (eGFR) ≥15 mL/min/1.73 m^2, and mild to moderate hepatic impairment (total bilirubin ≤3 times ULN and any AST). The effect of severe hepatic impairment (total bilirubin >3 times ULN and any AST) on pembrolizumab pharmacokinetics is unknown.

Pediatric Patients

Pembrolizumab exposures in pediatric patients 12 years and older who weigh greater than 40 kg are predicted to be within range of those observed in adult patients at the same dosage.

12.6 Immunogenicity

The observed incidence of anti-drug antibodies (ADA) is highly dependent on the sensitivity and specificity of the assay. Differences in assay methods preclude meaningful comparisons of the incidence of ADA in the studies described in this section with the incidence of ADA in other studies, including those of KEYTRUDA QLEX or of other pembrolizumab products or berahyaluronidase alfa products.

With a median (min, max) duration of treatment on KEYTRUDA QLEX of 6.9 months (1 day, 1 year) in Study MK-3475A-D77, 1.4% (3/211) of patients developed anti-pembrolizumab antibodies, and one ADA-positive patient developed neutralizing antibodies (NAb) against pembrolizumab. The incidence of anti-berahyaluronidase alfa antibodies was 1.5% (3/194). No analysis of neutralizing antibodies was performed for berahyaluronidase alfa ADA-positive samples. Because of the low occurrence of anti-pembrolizumab or anti-berahyaluronidase antibodies, the effect of these antibodies on the pharmacokinetics, safety and effectiveness of KEYTRUDA QLEX is unknown.

13 NONCLINICAL TOXICOLOGY

13.1 Carcinogenesis, Mutagenesis, Impairment of Fertility

KEYTRUDA QLEX contains pembrolizumab and berahyaluronidase alfa.

Pembrolizumab

No studies have been performed to test the potential of pembrolizumab for carcinogenicity or genotoxicity.

Fertility studies have not been conducted with pembrolizumab. In 1-month and 6-month repeat-dose toxicology studies in monkeys, there were no notable effects in the male and female reproductive organs; however, most animals in these studies were not sexually mature.

Berahyaluronidase alfa

Hyaluronidases are found in most tissues of the body. Long-term animal studies have not been performed to assess the carcinogenic or mutagenic potential of berahyaluronidase alfa.

In a fertility and early embryonic development study, male and female rats were administered daily subcutaneous injections of 280,000, 840,000, or 2,520,000 U/kg berahyaluronidase alfa. Males were dosed for 9 weeks prior to mating and throughout mating to termination. Females were dosed for 2 weeks prior to mating, throughout mating, and up to gestation day 7. Although treatment with ≥840,000 U/kg berahyaluronidase alfa (>5,200 times higher than the human dose) resulted in an increased incidence of abnormal sperm morphology, there were no adverse effects on mating, fertility or embryogenesis observed at doses up to 2,520,000 U/kg (>15,000 times higher than the human dose).

13.2 Animal Toxicology and/or Pharmacology

In animal models, inhibition of PD-1/PD-L1 signaling increased the severity of some infections and enhanced inflammatory responses. Mycobacterium tuberculosis-infected PD-1 knockout mice exhibit markedly decreased survival compared with wild-type controls, which correlated with increased bacterial proliferation and inflammatory responses in these animals. PD-1 blockade using a primate anti-PD-1 antibody was also shown to exacerbate M. tuberculosis infection in rhesus macaques. PD-1 and PD-L1 knockout mice and mice receiving PD-L1-blocking antibody have also shown decreased survival following infection with lymphocytic choriomeningitis virus. Administration of pembrolizumab in chimpanzees with naturally occurring chronic hepatitis B infection resulted in two out of four animals with significantly increased levels of serum ALT, AST, and GGT, which persisted for at least 1 month after discontinuation of pembrolizumab.

14 CLINICAL STUDIES

14.1 KEYTRUDA QLEX

NSCLC (Study MK-3475A-D77)

KEYTRUDA QLEX was evaluated in Study MK-3475A-D77 (NCT05722015), a randomized, multicenter, open-label, active-controlled trial conducted in patients with treatment-naïve metastatic NSCLC, in whom there were no EGFR, ALK, or ROS1 genomic tumor aberrations. Patients were excluded if they had a history of autoimmune disease that required systemic therapy within 2 years of treatment; had a medical condition that required immunosuppression; or had received more than 30 Gy of thoracic radiation within the prior 26 weeks.

A total of 377 patients were randomized (2:1) to receive either KEYTRUDA QLEX (containing 790 mg pembrolizumab and 9,600 units berahyaluronidase alfa) administered subcutaneously every 6 weeks with platinum doublet chemotherapy (n=251) or pembrolizumab 400 mg intravenously every 6 weeks with platinum doublet chemotherapy (n=126).

The chemotherapy regimens were as follows:

- Non-squamous NSCLC: pemetrexed 500 mg/m^2 and a platinum chemotherapy (cisplatin 75 mg/m^2 or carboplatin AUC 5 mg/mL/min) intravenously every 3 weeks for 4 cycles, followed by pemetrexed 500 mg/m^2 intravenously every 3 weeks.
- Squamous NSCLC: carboplatin AUC 6 mg/mL/min and a taxane (paclitaxel 200 mg/m^2 on Day 1 of each 21-day cycle or paclitaxel protein-bound 100 mg/m^2 on Days 1, 8 and 15 of each 21-day cycle) intravenously every 3 weeks for 4 cycles.

Randomization was stratified by ECOG performance status (0 vs. 1), histology (squamous vs. non-squamous), PD-L1 TPS (<50% vs. ≥50%), and geographic region (East Asia vs. North America/Western Europe/Australia/New Zealand vs. Rest of the World).

Treatment with KEYTRUDA QLEX or intravenous pembrolizumab continued until RECIST v1.1-defined progression of disease as determined by the investigator, unacceptable toxicity, or a maximum of 18 cycles (approximately 24 months). Administration of KEYTRUDA QLEX or intravenous pembrolizumab was permitted beyond RECIST-defined disease progression by BICR or beyond discontinuation of pemetrexed if the patient was clinically stable and deriving clinical benefit as determined by the investigator.

The primary outcome measure was pembrolizumab exposure [Cycle 1 AUC0-6 weeks and Cycle 3 (i.e., Steady State) Ctrough] of subcutaneous KEYTRUDA QLEX as compared to intravenous pembrolizumab [see Clinical Pharmacology (12.3)]. Additional descriptive efficacy outcome measures were overall response rate (ORR) by blinded independent central review (BICR), progression-free survival (PFS) by BICR, and overall survival (OS).

The study population characteristics were: median age 65 years (range: 37 to 87); 71% male; 63% White, 29% Asian, 4% multiracial, 3% Black or African American, 2% American Indian or Alaska Native; 31% of Hispanic or Latino ethnicity; 35% ECOG performance status (PS) of 0 and 65% ECOG PS of 1. Nineteen percent had PD-L1 TPS ≥50%; 34% had tumors with squamous histology and 66% had tumors with non-squamous histology; and 9% had brain metastases at baseline.

At the primary analysis, the confirmed ORR was 45% (95% CI: 39, 52) in the subcutaneous KEYTRUDA QLEX arm and 42% (95% CI: 33, 51) in the intravenous pembrolizumab arm. There were no notable differences in PFS or OS observed in patients who received KEYTRUDA QLEX compared to patients who received intravenous pembrolizumab.

Intravenous Pembrolizumab

The effectiveness of KEYTRUDA QLEX for its approved indications [see Indications and Usage (1)] has been established based upon the evidence from the adequate and well-controlled studies conducted with intravenous pembrolizumab [see Clinical Studies (14.2-14.20)] and additional data that demonstrated comparable pharmacokinetic, efficacy, and safety profiles between KEYTRUDA QLEX and intravenous pembrolizumab in Study MK-3475A-D77 [see Adverse Reactions (6.1), Clinical Pharmacology (12.3), and Clinical Studies (14.1)].

Below is a description of the efficacy results of these adequate and well-controlled studies of intravenous pembrolizumab in these patient populations.

14.2 Melanoma

Ipilimumab-Naive Melanoma

The efficacy of intravenous pembrolizumab was investigated in KEYNOTE-006 (NCT01866319), a randomized (1:1:1), open-label, multicenter, active-controlled trial in 834 patients. Patients were randomized to receive intravenous pembrolizumab at a dose of 10 mg/kg intravenously every 2 weeks or 10 mg/kg intravenously every 3 weeks until disease progression or unacceptable toxicity or to ipilimumab 3 mg/kg intravenously every 3 weeks for 4 doses unless discontinued earlier for disease progression or unacceptable toxicity. Patients with disease progression could receive additional doses of treatment unless disease progression was symptomatic, was rapidly progressive, required urgent intervention, occurred with a decline in performance status, or was confirmed at 4 to 6 weeks with repeat imaging. Randomization was stratified by line of therapy (0 vs. 1), ECOG PS (0 vs. 1), and PD-L1 expression (≥1% of tumor cells [positive] vs. <1% of tumor cells [negative]) according to an investigational use only (IUO) assay. Key eligibility criteria were unresectable or metastatic melanoma; no prior ipilimumab; and no more than one prior systemic treatment for metastatic melanoma. Patients with BRAF V600E mutation-positive melanoma were not required to have received prior BRAF inhibitor therapy. Patients with autoimmune disease; a medical condition that required immunosuppression; previous severe hypersensitivity to other monoclonal antibodies; and HIV, hepatitis B or hepatitis C infection, were ineligible. Assessment of tumor status was performed at 12 weeks, then every 6 weeks through Week 48, followed by every 12 weeks thereafter. The major efficacy outcome measures were overall survival (OS) and progression-free survival (PFS; as assessed by blinded independent central review [BICR] using Response Evaluation Criteria in Solid Tumors [RECIST v1.1, modified to follow a maximum of 10 target lesions and a maximum of 5 target lesions per organ]). Additional efficacy outcome measures were objective response rate (ORR) and duration of response (DoR).

The study population characteristics were: median age of 62 years (range: 18 to 89); 60% male; 98% White; 66% had no prior systemic therapy for metastatic disease; 69% ECOG PS of 0; 80% had PD-L1 positive melanoma, 18% had PD-L1 negative melanoma, and 2% had unknown PD-L1 status using the IUO assay; 65% had M1c stage disease; 68% with normal LDH; 36% with reported BRAF mutation-positive melanoma; and 9% with a history of brain metastases. Among patients with BRAF mutation-positive melanoma, 139 (46%) were previously treated with a BRAF inhibitor.

The study demonstrated statistically significant improvements in OS and PFS for patients randomized to intravenous pembrolizumab as compared to ipilimumab. Among the 91 patients randomized to intravenous pembrolizumab 10 mg/kg every 3 weeks with an objective response, response durations ranged from 1.4+ to 8.1+ months. Among the 94 patients randomized to intravenous pembrolizumab 10 mg/kg every 2 weeks with an objective response, response durations ranged from 1.4+ to 8.2 months. Efficacy results are summarized in Table 57 and Figure 1.

Table 57: Efficacy Results in KEYNOTE-006
Endpoint | Intravenous Pembrolizumab 10 mg/kg every 3 weeks n=277 | Intravenous Pembrolizumab 10 mg/kg every 2 weeks n=279 | Ipilimumab 3 mg/kg every 3 weeks n=278
OS
Deaths (%) | 92 (33%) | 85 (30%) | 112 (40%)
Hazard ratio [Hazard ratio (intravenous pembrolizumab compared to ipilimumab) based on the stratified Cox proportional hazard model] (95% CI) | 0.69 (0.52, 0.90) | 0.63 (0.47, 0.83) | ---
p-Value (stratified log-rank) | 0.004 | <0.001 | ---
PFS by BICR
Events (%) | 157 (57%) | 157 (56%) | 188 (68%)
Median in months (95% CI) | 4.1 (2.9, 6.9) | 5.5 (3.4, 6.9) | 2.8 (2.8, 2.9)
Hazard ratio (95% CI) | 0.58 (0.47, 0.72) | 0.58 (0.46, 0.72) | ---
p-Value (stratified log-rank) | <0.001 | <0.001 | ---
Best objective response by BICR
ORR (95% CI) | 33% (27, 39) | 34% (28, 40) | 12% (8, 16)
Complete response rate | 6% | 5% | 1%
Partial response rate | 27% | 29% | 10%

Figure 1: Kaplan-Meier Curve for Overall Survival in KEYNOTE-006 [Based on the final analysis with an additional follow-up of 9 months (total of 383 deaths as pre-specified in the protocol)]

Ipilimumab-Refractory Melanoma

The efficacy of intravenous pembrolizumab was investigated in KEYNOTE-002 (NCT01704287), a multicenter, randomized (1:1:1), active-controlled trial in 540 patients randomized to receive one of two doses of intravenous pembrolizumab in a blinded fashion or investigator's choice chemotherapy. The treatment arms consisted of intravenous pembrolizumab 2 mg/kg or 10 mg/kg intravenously every 3 weeks or investigator's choice of any of the following chemotherapy regimens: dacarbazine 1000 mg/m^2 intravenously every 3 weeks (26%), temozolomide 200 mg/m^2 orally once daily for 5 days every 28 days (25%), carboplatin AUC 6 mg/mL/min intravenously plus paclitaxel 225 mg/m^2 intravenously every 3 weeks for four cycles then carboplatin AUC of 5 mg/mL/min plus paclitaxel 175 mg/m^2 every 3 weeks (25%), paclitaxel 175 mg/m^2 intravenously every 3 weeks (16%), or carboplatin AUC 5 or 6 mg/mL/min intravenously every 3 weeks (8%). Randomization was stratified by ECOG PS (0 vs. 1), LDH levels (normal vs. elevated [≥110% ULN]) and BRAF V600 mutation status (wild-type [WT] or V600E). The trial included patients with unresectable or metastatic melanoma with progression of disease; refractory to two or more doses of ipilimumab (3 mg/kg or higher) and, if BRAF V600 mutation-positive, a BRAF or MEK inhibitor; and disease progression within 24 weeks following the last dose of ipilimumab. The trial excluded patients with uveal melanoma and active brain metastasis. Patients received intravenous pembrolizumab until unacceptable toxicity; disease progression that was symptomatic, was rapidly progressive, required urgent intervention, occurred with a decline in performance status, or was confirmed at 4 to 6 weeks with repeat imaging; withdrawal of consent; or physician's decision to stop therapy for the patient. Assessment of tumor status was performed at 12 weeks after randomization, then every 6 weeks through week 48, followed by every 12 weeks thereafter. Patients on chemotherapy who experienced progression of disease were offered intravenous pembrolizumab. The major efficacy outcomes were PFS as assessed by BICR per RECIST v1.1, modified to follow a maximum of 10 target lesions and a maximum of 5 target lesions per organ, and OS. Additional efficacy outcome measures were confirmed ORR as assessed by BICR per RECIST v1.1, modified to follow a maximum of 10 target lesions and a maximum of 5 target lesions per organ, and DoR.

The study population characteristics were: median age of 62 years (range: 15 to 89), 43% age 65 or older; 61% male; 98% White; and 55% ECOG PS of 0 and 45% ECOG PS of 1. Twenty-three percent of patients were BRAF V600 mutation positive, 40% had elevated LDH at baseline, 82% had M1c disease, and 73% had two or more prior therapies for advanced or metastatic disease.

The study demonstrated a statistically significant improvement in PFS for patients randomized to intravenous pembrolizumab as compared to control arm. There was no statistically significant difference between intravenous pembrolizumab 2 mg/kg and chemotherapy or between intravenous pembrolizumab 10 mg/kg and chemotherapy in the OS analysis in which 55% of the patients who had been randomized to receive chemotherapy had crossed over to receive intravenous pembrolizumab. Among the 38 patients randomized to intravenous pembrolizumab 2 mg/kg with an objective response, response durations ranged from 1.3+ to 11.5+ months. Among the 46 patients randomized to intravenous pembrolizumab 10 mg/kg with an objective response, response durations ranged from 1.1+ to 11.1+ months. Efficacy results are summarized in Table 58 and Figure 2.

Table 58: Efficacy Results in KEYNOTE-002
Endpoint | Intravenous Pembrolizumab 2 mg/kg every 3 weeks | Intravenous Pembrolizumab 10 mg/kg every 3 weeks | Chemotherapy
 | n=180 | n=181 | n=179
PFS
Number of Events, n (%) | 129 (72%) | 126 (70%) | 155 (87%)
Progression, n (%) | 105 (58%) | 107 (59%) | 134 (75%)
Death, n (%) | 24 (13%) | 19 (10%) | 21 (12%)
Median in months (95% CI) | 2.9 (2.8, 3.8) | 2.9 (2.8, 4.7) | 2.7 (2.5, 2.8)
p-Value (stratified log-rank) | <0.001 | <0.001 | ---
Hazard ratio [Hazard ratio (intravenous pembrolizumab compared to chemotherapy) based on the stratified Cox proportional hazard model] (95% CI) | 0.57 (0.45, 0.73) | 0.50 (0.39, 0.64) | ---
OS [With additional follow-up of 18 months after the PFS analysis]
Deaths (%) | 123 (68%) | 117 (65%) | 128 (72%)
Hazard ratio (95% CI) | 0.86 (0.67, 1.10) | 0.74 (0.57, 0.96) | ---
p-Value (stratified log-rank) | 0.117 | 0.011 [Not statistically significant compared to multiplicity adjusted significance level of 0.01] | ---
Median in months (95% CI) | 13.4 (11.0, 16.4) | 14.7 (11.3, 19.5) | 11.0 (8.9, 13.8)
Objective Response Rate
ORR (95% CI) | 21% (15, 28) | 25% (19, 32) | 4% (2, 9)
Complete response rate | 2% | 3% | 0%
Partial response rate | 19% | 23% | 4%

Figure 2: Kaplan-Meier Curve for Progression-Free Survival in KEYNOTE-002

Adjuvant Treatment of Resected Stage IIB or IIC Melanoma

The efficacy of intravenous pembrolizumab was investigated in KEYNOTE-716 (NCT03553836), a multicenter, randomized (1:1), double-blind, placebo-controlled trial in patients with completely resected Stage IIB or IIC melanoma. Patients were randomized to intravenous pembrolizumab 200 mg or the pediatric (≥12 years old) dose of intravenous pembrolizumab 2 mg/kg intravenously (up to a maximum of 200 mg) every three weeks or placebo for up to one year until disease recurrence or unacceptable toxicity. Randomization was stratified by AJCC 8th edition T Stage (>2.0-4.0 mm with ulceration vs. >4.0 mm without ulceration vs. >4.0 mm with ulceration). Patients must not have been previously treated for melanoma beyond complete surgical resection for their melanoma prior to study entry. The major efficacy outcome measure was investigator-assessed recurrence-free survival (RFS) (defined as the time between the date of randomization and the date of first recurrence [local, in-transit or regional lymph nodes or distant recurrence] or death, whichever occurred first). New primary melanomas were excluded from the definition of RFS. Distant metastasis-free survival (DMFS), defined as a spread of tumor to distant organs or distant lymph nodes, was an additional efficacy outcome measure. Patients underwent imaging every six months for one year from randomization, every 6 months from years 2 to 4, and then once in year 5 from randomization or until recurrence, whichever came first.

The study population characteristics were: median age of 61 years (range: 16 to 87), 39% age 65 or older; 60% male; 98% White; and 93% ECOG PS of 0 and 7% ECOG PS of 1. Sixty-four percent had Stage IIB and 35% had Stage IIC.

The trial demonstrated a statistically significant improvement in RFS and DMFS for patients randomized to the intravenous pembrolizumab arm compared with placebo. Efficacy results are summarized in Table 59 and Figure 3.

Table 59: Efficacy Results in KEYNOTE-716
Endpoint | Intravenous Pembrolizumab 200 mg every 3 weeks n=487 | Placebo n=489
RFS
Number (%) of patients with event | 54 (11%) | 82 (17%)
Median in months (95% CI) | NR (22.6, NR) | NR (NR, NR)
Hazard ratio [Based on the stratified Cox proportional hazard model] , [Based on a log-rank test stratified by American Joint Committee on Cancer 8th edition (AJCC) stage] (95% CI) | 0.65 (0.46, 0.92)
p-Value | 0.0132 [p-Value is compared with 0.0202 of the allocated alpha for this interim analysis.]
DMFS
Number (%) of patients with event | 63 (13%) | 95 (19%)
Median in months (95% CI) | NR (NR, NR) | NR (NR, NR)
Hazard ratio, (95% CI) | 0.64 (0.47, 0.88)
p-Value | 0.0058 [p-Value is compared with 0.0256 of the allocated alpha for this interim analysis.]
NR = not reached

Figure 3: Kaplan-Meier Curve for Recurrence-Free Survival in KEYNOTE-716

Adjuvant Treatment of Stage III Resected Melanoma

The efficacy of intravenous pembrolizumab was investigated in KEYNOTE-054 (NCT02362594), a multicenter, randomized (1:1), double-blind, placebo-controlled trial in patients with completely resected Stage IIIA (>1 mm lymph node metastasis), IIIB, or IIIC melanoma. Patients were randomized to intravenous pembrolizumab 200 mg intravenously every three weeks or placebo for up to one year until disease recurrence or unacceptable toxicity. Randomization was stratified by American Joint Committee on Cancer 7th edition (AJCC) stage (IIIA vs. IIIB vs. IIIC 1-3 positive lymph nodes vs. IIIC ≥4 positive lymph nodes) and geographic region (North America, European countries, Australia, and other countries as designated). Patients must have undergone lymph node dissection and, if indicated, radiotherapy within 13 weeks prior to starting treatment. The major efficacy outcome measure was investigator-assessed recurrence-free survival (RFS) in the whole population and in the population with PD-L1 positive tumors where RFS was defined as the time between the date of randomization and the date of first recurrence (local, regional, or distant metastasis) or death, whichever occurs first. New primary melanomas were excluded from the definition of RFS. DMFS in the whole population and in the population with PD-L1 positive tumors were additional efficacy outcome measures. DMFS was defined as a spread of tumor to distant organs or distant lymph nodes. Patients underwent imaging every 12 weeks after the first dose of intravenous pembrolizumab for the first two years, then every 6 months from year 3 to 5, and then annually.

The study population characteristics were: median age of 54 years (range: 19 to 88), 25% age 65 or older; 62% male; and 94% ECOG PS of 0 and 6% ECOG PS of 1. Sixteen percent had Stage IIIA, 46% had Stage IIIB, 18% had Stage IIIC (1-3 positive lymph nodes), and 20% had Stage IIIC (≥4 positive lymph nodes); 50% were BRAF V600 mutation positive and 44% were BRAF wild-type; and 84% had PD-L1 positive melanoma with TPS ≥1% according to an IUO assay.

The trial demonstrated a statistically significant improvement in RFS and DMFS for patients randomized to the intravenous pembrolizumab arm compared with placebo. Efficacy results are summarized in Table 60 and Figure 4.

Table 60: Efficacy Results in KEYNOTE-054
Endpoint | Intravenous Pembrolizumab 200 mg every 3 weeks n=514 | Placebo n=505
RFS
Number (%) of patients with event | 135 (26%) | 216 (43%)
Median in months (95% CI) | NR | 20.4 (16.2, NR)
Hazard ratio [Based on the stratified Cox proportional hazard model] , [Stratified by American Joint Committee on Cancer 7th edition (AJCC) stage] (95% CI) | 0.57 (0.46, 0.70)
p-Value (log-rank) | <0.001 [p-Value is compared with 0.016 of the allocated alpha for this interim analysis.]
DMFS
Number (%) of patients with event | 173 (34%) | 245 (49%)
Median in months (95% CI) | NR (49.6, NR) | 40.0 (27.7, NR)
Hazard ratio, (95% CI) | 0.60 (0.49, 0.73)
p-Value (log-rank) | <0.0001 [p-Value is compared with 0.028 of the allocated alpha for this analysis.]
NR = not reached

For patients with PD-L1 positive tumors, the RFS HR was 0.54 (95% CI: 0.42, 0.69); p<0.0001. For patients with PD-L1 positive tumors, the DMFS HR was 0.61 (95% CI: 0.49, 0.76); p<0.0001. The RFS and DMFS benefit for intravenous pembrolizumab compared to placebo was observed regardless of tumor PD-L1 expression.

Figure 4: Kaplan-Meier Curve for Recurrence-Free Survival in KEYNOTE-054

14.3 Non-Small Cell Lung Cancer

First-line treatment of metastatic nonsquamous NSCLC with pemetrexed and platinum chemotherapy

The efficacy of intravenous pembrolizumab in combination with pemetrexed and platinum chemotherapy was investigated in KEYNOTE-189 (NCT02578680), a randomized, multicenter, double-blind, active-controlled trial conducted in 616 patients with metastatic nonsquamous NSCLC, regardless of PD-L1 tumor expression status, who had not previously received systemic therapy for metastatic disease and in whom there were no EGFR or ALK genomic tumor aberrations. Patients with autoimmune disease that required systemic therapy within 2 years of treatment; a medical condition that required immunosuppression; or who had received more than 30 Gy of thoracic radiation within the prior 26 weeks were ineligible. Randomization was stratified by smoking status (never vs. former/current), choice of platinum (cisplatin vs. carboplatin), and tumor PD-L1 status (TPS <1% [negative] vs. TPS ≥1%). Patients were randomized (2:1) to one of the following treatment arms:

- Intravenous pembrolizumab 200 mg, pemetrexed 500 mg/m^2, and investigator's choice of cisplatin 75 mg/m^2 or carboplatin AUC 5 mg/mL/min intravenously on Day 1 of each 21-day cycle for 4 cycles followed by intravenous pembrolizumab 200 mg and pemetrexed 500 mg/m^2 intravenously every 3 weeks.
- Placebo, pemetrexed 500 mg/m^2, and investigator's choice of cisplatin 75 mg/m^2 or carboplatin AUC 5 mg/mL/min intravenously on Day 1 of each 21-day cycle for 4 cycles followed by placebo and pemetrexed 500 mg/m^2 intravenously every 3 weeks.

Treatment with intravenous pembrolizumab continued until RECIST v1.1 (modified to follow a maximum of 10 target lesions and a maximum of 5 target lesions per organ)-defined progression of disease as determined by the investigator, unacceptable toxicity, or a maximum of 24 months. Administration of intravenous pembrolizumab was permitted beyond RECIST-defined disease progression if the patient was clinically stable and considered to be deriving clinical benefit by the investigator. Patients randomized to placebo and chemotherapy were offered intravenous pembrolizumab as a single agent at the time of disease progression. Assessment of tumor status was performed at Week 6, Week 12, and then every 9 weeks thereafter. The main efficacy outcome measures were OS and PFS as assessed by BICR according to RECIST v1.1, modified to follow a maximum of 10 target lesions and a maximum of 5 target lesions per organ. Additional efficacy outcome measures were ORR and DoR, as assessed by BICR according to RECIST v1.1, modified to follow a maximum of 10 target lesions and a maximum of 5 target lesions per organ.

The study population characteristics were: median age of 64 years (range: 34 to 84), 49% age 65 or older; 59% male; 94% White and 3% Asian; 56% ECOG PS of 1; and 18% with history of brain metastases. Thirty-one percent had tumor PD-L1 expression TPS <1% [negative]. Seventy-two percent received carboplatin and 12% were never smokers. A total of 85 patients in the placebo and chemotherapy arm received an anti-PD-1/PD-L1 monoclonal antibody at the time of disease progression.

The trial demonstrated a statistically significant improvement in OS and PFS for patients randomized to intravenous pembrolizumab in combination with pemetrexed and platinum chemotherapy compared with placebo, pemetrexed, and platinum chemotherapy. Table 61 and Figure 5 summarize the efficacy results for KEYNOTE-189.

Table 61: Efficacy Results in KEYNOTE-189
Endpoint | Intravenous Pembrolizumab 200 mg every 3 weeks Pemetrexed Platinum Chemotherapy n=410 | Placebo Pemetrexed Platinum Chemotherapy n=206
OS
Number (%) of patients with event | 127 (31%) | 108 (52%)
Median in months (95% CI) | NR (NR, NR) | 11.3 (8.7, 15.1)
Hazard ratio [Based on the stratified Cox proportional hazard model] (95% CI) | 0.49 (0.38, 0.64)
p-Value [Based on a stratified log-rank test] | <0.0001
PFS
Number of patients with event (%) | 245 (60%) | 166 (81%)
Median in months (95% CI) | 8.8 (7.6, 9.2) | 4.9 (4.7, 5.5)
Hazard ratio (95% CI) | 0.52 (0.43, 0.64)
p-Value | <0.0001
Objective Response Rate
ORR [Response: Best objective response as confirmed complete response or partial response] (95% CI) | 48% (43, 53) | 19% (14, 25)
Complete response | 0.5% | 0.5%
Partial response | 47% | 18%
p-Value [Based on Miettinen and Nurminen method stratified by PD-L1 status, platinum chemotherapy, and smoking status] | <0.0001
Duration of Response
Median in months (range) | 11.2 (1.1+, 18.0+) | 7.8 (2.1+, 16.4+)
NR = not reached

At the protocol-specified final OS analysis, the median in the intravenous pembrolizumab in combination with pemetrexed and platinum chemotherapy arm was 22.0 months (95% CI: 19.5, 24.5) compared to 10.6 months (95% CI: 8.7, 13.6) in the placebo with pemetrexed and platinum chemotherapy arm, with an HR of 0.56 (95% CI: 0.46, 0.69).

Figure 5: Kaplan-Meier Curve for Overall Survival in KEYNOTE-189 [Based on the protocol-specified final OS analysis]

First-line treatment of metastatic squamous NSCLC with carboplatin and either paclitaxel or paclitaxel protein-bound chemotherapy

The efficacy of intravenous pembrolizumab in combination with carboplatin and investigator's choice of either paclitaxel or paclitaxel protein-bound was investigated in KEYNOTE-407 (NCT02775435), a randomized, multi-center, double-blind, placebo-controlled trial conducted in 559 patients with metastatic squamous NSCLC, regardless of PD-L1 tumor expression status, who had not previously received systemic therapy for metastatic disease. Patients with autoimmune disease that required systemic therapy within 2 years of treatment; a medical condition that required immunosuppression; or who had received more than 30 Gy of thoracic radiation within the prior 26 weeks were ineligible. Randomization was stratified by tumor PD-L1 status (TPS <1% [negative] vs. TPS ≥1%), choice of paclitaxel or paclitaxel protein-bound, and geographic region (East Asia vs. non-East Asia). Patients were randomized (1:1) to one of the following treatment arms; all study medications were administered via intravenous infusion:

- Intravenous pembrolizumab 200 mg and carboplatin AUC 6 mg/mL/min on Day 1 of each 21-day cycle for 4 cycles, and paclitaxel 200 mg/m^2 on Day 1 of each 21-day cycle for 4 cycles or paclitaxel protein-bound 100 mg/m^2 on Days 1, 8 and 15 of each 21-day cycle for 4 cycles, followed by intravenous pembrolizumab 200 mg every 3 weeks.
- Placebo and carboplatin AUC 6 mg/mL/min on Day 1 of each 21-day cycle for 4 cycles and paclitaxel 200 mg/m^2 on Day 1 of each 21-day cycle for 4 cycles or paclitaxel protein-bound 100 mg/m^2 on Days 1, 8 and 15 of each 21-day cycle for 4 cycles, followed by placebo every 3 weeks.

Treatment with intravenous pembrolizumab and chemotherapy or placebo and chemotherapy continued until RECIST v1.1 (modified to follow a maximum of 10 target lesions and a maximum of 5 target lesions per organ)-defined progression of disease as determined by BICR, unacceptable toxicity, or a maximum of 24 months. Administration of intravenous pembrolizumab was permitted beyond RECIST-defined disease progression if the patient was clinically stable and deriving clinical benefit as determined by the investigator. Patients randomized to the placebo and chemotherapy arm were offered intravenous pembrolizumab as a single agent at the time of disease progression. Assessment of tumor status was performed every 6 weeks through Week 18, every 9 weeks through Week 45 and every 12 weeks thereafter. The main efficacy outcome measures were PFS and ORR as assessed by BICR using RECIST v1.1, modified to follow a maximum of 10 target lesions and a maximum of 5 target lesions per organ, and OS. An additional efficacy outcome measure was DoR as assessed by BICR according to RECIST v1.1, modified to follow a maximum of 10 target lesions and a maximum of 5 target lesions per organ.

The study population characteristics were: median age of 65 years (range: 29 to 88), 55% age 65 or older; 81% male; 77% White; 71% ECOG PS of 1; and 8% with a history of brain metastases. Thirty-five percent had tumor PD-L1 expression TPS <1%; 19% were from the East Asian region; and 60% received paclitaxel.

The trial demonstrated a statistically significant improvement in OS, PFS and ORR in patients randomized to intravenous pembrolizumab in combination with carboplatin and either paclitaxel or paclitaxel protein-bound chemotherapy compared with patients randomized to placebo with carboplatin and either paclitaxel or paclitaxel protein-bound chemotherapy. Table 62 and Figure 6 summarize the efficacy results for KEYNOTE-407.

Table 62: Efficacy Results in KEYNOTE-407
Endpoint | Intravenous Pembrolizumab 200 mg every 3 weeks Carboplatin Paclitaxel/Paclitaxel protein-bound n=278 | Placebo Carboplatin Paclitaxel/Paclitaxel protein-bound n=281
OS
Number of events (%) | 85 (31%) | 120 (43%)
Median in months (95% CI) | 15.9 (13.2, NE) | 11.3 (9.5, 14.8)
Hazard ratio [Based on the stratified Cox proportional hazard model] (95% CI) | 0.64 (0.49, 0.85)
p-Value [Based on a stratified log-rank test] | 0.0017
PFS
Number of events (%) | 152 (55%) | 197 (70%)
Median in months (95% CI) | 6.4 (6.2, 8.3) | 4.8 (4.2, 5.7)
Hazard ratio (95% CI) | 0.56 (0.45, 0.70)
p-Value | <0.0001
 | n=101 | n=103
Objective Response Rate [ORR primary analysis and DoR analysis were conducted with the first 204 patients enrolled.]
ORR (95% CI) | 58% (48, 68) | 35% (26, 45)
Difference (95% CI) | 23.6% (9.9, 36.4)
p-Value [Based on a stratified Miettinen-Nurminen test] | 0.0008
Duration of Response
Median duration of response in months (range) | 7.2 (2.4, 12.4+) | 4.9 (2.0, 12.4+)
NE = not estimable

At the protocol-specified final OS analysis, the median in the intravenous pembrolizumab in combination with carboplatin and either paclitaxel or paclitaxel protein-bound chemotherapy arm was 17.1 months (95% CI: 14.4, 19.9) compared to 11.6 months (95% CI: 10.1, 13.7) in the placebo with carboplatin and either paclitaxel or paclitaxel protein-bound chemotherapy arm, with an HR of 0.71 (95% CI: 0.58, 0.88).

Figure 6: Kaplan-Meier Curve for Overall Survival in KEYNOTE-407 [Based on the protocol-specified final OS analysis]

First-line treatment of metastatic NSCLC with PD-L1 expression (TPS ≥1%) as a single agent

KEYNOTE-042

The efficacy of intravenous pembrolizumab was investigated in KEYNOTE-042 (NCT02220894), a randomized, multicenter, open-label, active-controlled trial conducted in 1274 patients with Stage III NSCLC who were not candidates for surgical resection or definitive chemoradiation, or patients with metastatic NSCLC. Only patients whose tumors expressed PD-L1 (TPS ≥1%) by an immunohistochemistry assay using the PD-L1 IHC 22C3 pharmDx assay and who had not received prior systemic treatment for metastatic NSCLC were eligible. Patients with EGFR or ALK genomic tumor aberrations; autoimmune disease that required systemic therapy within 2 years of treatment; a medical condition that required immunosuppression; or who had received more than 30 Gy of radiation in the thoracic region within the prior 26 weeks of initiation of study were ineligible. Randomization was stratified by ECOG PS (0 vs. 1), histology (squamous vs. nonsquamous), geographic region (East Asia vs. non-East Asia), and PD-L1 expression (TPS ≥50% vs. TPS 1 to 49%). Patients were randomized (1:1) to receive intravenous pembrolizumab 200 mg intravenously every 3 weeks or investigator's choice of either of the following platinum-containing chemotherapy regimens:

- Pemetrexed 500 mg/m^2 every 3 weeks and carboplatin AUC 5 to 6 mg/mL/min every 3 weeks on Day 1 for a maximum of 6 cycles followed by optional pemetrexed 500 mg/m^2 every 3 weeks for patients with nonsquamous histologies;
- Paclitaxel 200 mg/m^2 every 3 weeks and carboplatin AUC 5 to 6 mg/mL/min every 3 weeks on Day 1 for a maximum of 6 cycles followed by optional pemetrexed 500 mg/m^2 every 3 weeks for patients with nonsquamous histologies.

Treatment with intravenous pembrolizumab continued until RECIST v1.1 (modified to follow a maximum of 10 target lesions and a maximum of 5 target lesions per organ)-defined progression of disease, unacceptable toxicity, or a maximum of 24 months. Administration of intravenous pembrolizumab was permitted beyond RECIST-defined disease progression if the patient was clinically stable and deriving clinical benefit as determined by the investigator. Treatment with intravenous pembrolizumab could be reinitiated at the time of subsequent disease progression and administered for up to 12 months. Assessment of tumor status was performed every 9 weeks. The main efficacy outcome measure was OS in the subgroup of patients with TPS ≥50% NSCLC, the subgroup of patients with TPS ≥20% NSCLC, and the overall population with TPS ≥1% NSCLC. Additional efficacy outcome measures were PFS and ORR in the subgroup of patients with TPS ≥50% NSCLC, the subgroup of patients with TPS ≥20% NSCLC, and the overall population with TPS ≥1% NSCLC as assessed by BICR according to RECIST v1.1, modified to follow a maximum of 10 target lesions and a maximum of 5 target lesions per organ.

The study population characteristics were: median age of 63 years (range: 25 to 90), 45% age 65 or older; 71% male; and 64% White, 30% Asian, and 2% Black. Nineteen percent were Hispanic or Latino. Sixty-nine percent had ECOG PS of 1; 39% with squamous and 61% with nonsquamous histology; 87% had M1 disease and 13% had Stage IIIA (2%) or Stage IIIB (11%) and who were not candidates for surgical resection or definitive chemoradiation per investigator assessment; and 5% with treated brain metastases at baseline. Forty-seven percent of patients had TPS ≥50% NSCLC and 53% had TPS 1 to 49% NSCLC.

The trial demonstrated a statistically significant improvement in OS for patients (PD-L1 TPS ≥50%, TPS ≥20%, TPS ≥1%) randomized to intravenous pembrolizumab as compared with chemotherapy. Table 63 and Figure 7 summarize the efficacy results in the subgroup of patients with TPS ≥50% and in all randomized patients with TPS ≥1%.

Table 63: Efficacy Results of All Randomized Patients (TPS ≥1% and TPS ≥50%) in KEYNOTE-042
 | TPS ≥1% |  | TPS ≥50%
Endpoint | Intravenous Pembrolizumab 200 mg every 3 weeks | Chemotherapy | Intravenous Pembrolizumab 200 mg every 3 weeks | Chemotherapy
Endpoint | n=637 | n=637 | n=299 | n=300
OS
Number of events (%) | 371 (58%) | 438 (69%) | 157 (53%) | 199 (66%)
Median in months (95% CI) | 16.7 (13.9, 19.7) | 12.1 (11.3, 13.3) | 20.0 (15.4, 24.9) | 12.2 (10.4, 14.2)
Hazard ratio [Based on the stratified Cox proportional hazard model] (95% CI) | 0.81 (0.71, 0.93) |  | 0.69 (0.56, 0.85)
p-Value [Based on a stratified log-rank test; compared to a p-Value boundary of 0.0291] | 0.0036 |  | 0.0006
PFS
Number of events (%) | 507 (80%) | 506 (79%) | 221 (74%) | 233 (78%)
Median in months (95% CI) | 5.4 (4.3, 6.2) | 6.5 (6.3, 7.0) | 6.9 (5.9, 9.0) | 6.4 (6.1, 6.9)
Hazard ratio, [Not evaluated for statistical significance as a result of the sequential testing procedure for the secondary endpoints] (95% CI) | 1.07 (0.94, 1.21) |  | 0.82 (0.68, 0.99)
p-Value | - |  | NS [Not significant compared to a p-Value boundary of 0.0291]
Objective Response Rate
ORR (95% CI) | 27% (24, 31) | 27% (23, 30) | 39% (33.9, 45.3) | 32% (26.8, 37.6)
Complete response rate | 0.5% | 0.5% | 0.7% | 0.3%
Partial response rate | 27% | 26% | 39% | 32%
Duration of Response
% with duration ≥12 months [Based on observed duration of response] | 47% | 16% | 42% | 17%
% with duration ≥18 months | 26% | 6% | 25% | 5%

The results of all efficacy outcome measures in the subgroup of patients with PD-L1 TPS ≥20% NSCLC were intermediate between the results of those with PD-L1 TPS ≥1% and those with PD-L1 TPS ≥50%. In a pre-specified exploratory subgroup analysis for patients with TPS 1-49% NSCLC, the median OS was 13.4 months (95% CI: 10.7, 18.2) for the pembrolizumab group and 12.1 months (95% CI: 11.0, 14.0) in the chemotherapy group, with an HR of 0.92 (95% CI: 0.77, 1.11).

Figure 7: Kaplan-Meier Curve for Overall Survival in all Randomized Patients in KEYNOTE-042 (TPS ≥1%)

KEYNOTE-024

The efficacy of intravenous pembrolizumab was also investigated in KEYNOTE-024 (NCT02142738), a randomized, multicenter, open-label, active-controlled trial in 305 previously untreated patients with metastatic NSCLC. The study design was similar to that of KEYNOTE-042, except that only patients whose tumors had high PD-L1 expression (TPS of 50% or greater) by an immunohistochemistry assay using the PD-L1 IHC 22C3 pharmDx assay were eligible. Patients were randomized (1:1) to receive intravenous pembrolizumab 200 mg intravenously every 3 weeks or investigator's choice of any of the following platinum-containing chemotherapy regimens:

- Pemetrexed 500 mg/m^2 every 3 weeks and carboplatin AUC 5 to 6 mg/mL/min every 3 weeks on Day 1 for 4 to 6 cycles followed by optional pemetrexed 500 mg/m^2 every 3 weeks for patients with nonsquamous histologies;
- Pemetrexed 500 mg/m^2 every 3 weeks and cisplatin 75 mg/m^2 every 3 weeks on Day 1 for 4 to 6 cycles followed by optional pemetrexed 500 mg/m^2 every 3 weeks for patients with nonsquamous histologies;
- Gemcitabine 1250 mg/m^2 on days 1 and 8 and cisplatin 75 mg/m^2 every 3 weeks on Day 1 for 4 to 6 cycles;
- Gemcitabine 1250 mg/m^2 on Days 1 and 8 and carboplatin AUC 5 to 6 mg/mL/min every 3 weeks on Day 1 for 4 to 6 cycles;
- Paclitaxel 200 mg/m^2 every 3 weeks and carboplatin AUC 5 to 6 mg/mL/min every 3 weeks on Day 1 for 4 to 6 cycles followed by optional pemetrexed maintenance (for nonsquamous histologies).

Patients randomized to chemotherapy were offered intravenous pembrolizumab at the time of disease progression.

The main efficacy outcome measure was PFS as assessed by BICR according to RECIST v1.1, modified to follow a maximum of 10 target lesions and a maximum of 5 target lesions per organ. Additional efficacy outcome measures were OS and ORR as assessed by BICR according to RECIST v1.1, modified to follow a maximum of 10 target lesions and a maximum of 5 target lesions per organ.

The study population characteristics were: median age of 65 years (range: 33 to 90), 54% age 65 or older; 61% male; 82% White and 15% Asian; 65% with ECOG PS of 1; 18% with squamous and 82% with nonsquamous histology and 9% with history of brain metastases. A total of 66 patients in the chemotherapy arm received intravenous pembrolizumab at the time of disease progression.

The trial demonstrated a statistically significant improvement in both PFS and OS for patients randomized to intravenous pembrolizumab as compared with chemotherapy. Table 64 and Figure 8 summarize the efficacy results for KEYNOTE-024.

Table 64: Efficacy Results in KEYNOTE-024
Endpoint | Intravenous Pembrolizumab 200 mg every 3 weeks | Chemotherapy
 | n=154 | n=151
PFS
Number (%) of patients with event | 73 (47%) | 116 (77%)
Median in months (95% CI) | 10.3 (6.7, NR) | 6.0 (4.2, 6.2)
Hazard ratio [Based on the stratified Cox proportional hazard model for the interim analysis] (95% CI) | 0.50 (0.37, 0.68)
p-Value (stratified log-rank) | <0.001
OS
Number (%) of patients with event | 44 (29%) | 64 (42%)
Median in months (95% CI) [Based on the protocol-specified final OS analysis conducted at 169 events, which occurred 14 months after the interim analysis.] | 30.0 (18.3, NR) | 14.2 (9.8, 19.0)
Hazard ratio (95% CI) | 0.60 (0.41, 0.89)
p-Value (stratified log-rank) | 0.005 [p-Value is compared with 0.0118 of the allocated alpha for the interim analysis]
Objective Response Rate
ORR (95% CI) | 45% (37, 53) | 28% (21, 36)
Complete response rate | 4% | 1%
Partial response rate | 41% | 27%
p-Value (Miettinen-Nurminen) | 0.001
Median duration of response in months (range) | NR (1.9+, 14.5+) | 6.3 (2.1+, 12.6+)
NR = not reached

Figure 8: Kaplan-Meier Curve for Overall Survival in KEYNOTE-024 [Based on the protocol-specified final OS analysis conducted at 169 events, which occurred 14 months after the interim analysis.]

Previously treated NSCLC with PD-L1 expression (TPS ≥1%)

The efficacy of intravenous pembrolizumab was investigated in KEYNOTE-010 (NCT01905657), a randomized, multicenter, open-label, active-controlled trial conducted in 1033 patients with metastatic NSCLC that had progressed following platinum-containing chemotherapy, and if appropriate, targeted therapy for EGFR or ALK genomic tumor aberrations. Eligible patients had PD-L1 expression TPS of 1% or greater by an immunohistochemistry assay using the PD-L1 IHC 22C3 pharmDx assay. Patients with autoimmune disease; a medical condition that required immunosuppression; or who had received more than 30 Gy of thoracic radiation within the prior 26 weeks were ineligible. Randomization was stratified by tumor PD-L1 expression (PD-L1 expression TPS ≥50% vs. PD-L1 expression TPS=1-49%), ECOG PS (0 vs. 1), and geographic region (East Asia vs. non-East Asia). Patients were randomized (1:1:1) to receive intravenous pembrolizumab 2 mg/kg intravenously every 3 weeks, intravenous pembrolizumab 10 mg/kg intravenously every 3 weeks or docetaxel intravenously 75 mg/m^2 every 3 weeks until unacceptable toxicity or disease progression. Patients randomized to intravenous pembrolizumab were permitted to continue until disease progression that was symptomatic, rapidly progressive, required urgent intervention, occurred with a decline in performance status, or confirmation of progression at 4 to 6 weeks with repeat imaging or for up to 24 months without disease progression. Assessment of tumor status was performed every 9 weeks. The main efficacy outcome measures were OS and PFS as assessed by BICR according to RECIST v1.1, modified to follow a maximum of 10 target lesions and a maximum of 5 target lesions per organ, in the subgroup of patients with TPS ≥50% and the overall population with TPS ≥1%. Additional efficacy outcome measures were ORR and DoR in the subgroup of patients with TPS ≥50% and the overall population with TPS ≥1%.

The study population characteristics were: median age of 63 years (range: 20 to 88), 42% age 65 or older; 61% male; 72% White and 21% Asian; 66% ECOG PS of 1; 43% with high PD-L1 tumor expression; 21% with squamous, 70% with nonsquamous, and 8% with mixed, other or unknown histology; 91% metastatic (M1) disease; 15% with history of brain metastases; and 8% and 1% with EGFR and ALK genomic aberrations, respectively. All patients had received prior therapy with a platinum-doublet regimen, 29% received two or more prior therapies for their metastatic disease.

Tables 65 and 66 and Figure 9 summarize efficacy results in the subgroup with TPS ≥50% population and in all patients, respectively.

Table 65: Efficacy Results of the Subgroup of Patients with TPS ≥50% in KEYNOTE-010
Endpoint | Intravenous Pembrolizumab 2 mg/kg every 3 weeks n=139 | Intravenous Pembrolizumab 10 mg/kg every 3 weeks n=151 | Docetaxel 75 mg/m^2 every 3 weeks n=152
OS
Deaths (%) | 58 (42%) | 60 (40%) | 86 (57%)
Median in months (95% CI) | 14.9 (10.4, NR) | 17.3 (11.8, NR) | 8.2 (6.4, 10.7)
Hazard ratio [Hazard ratio (intravenous pembrolizumab compared to docetaxel) based on the stratified Cox proportional hazard model] (95% CI) | 0.54 (0.38, 0.77) | 0.50 (0.36, 0.70) | ---
p-Value (stratified log-rank) | <0.001 | <0.001 | ---
PFS
Events (%) | 89 (64%) | 97 (64%) | 118 (78%)
Median in months (95% CI) | 5.2 (4.0, 6.5) | 5.2 (4.1, 8.1) | 4.1 (3.6, 4.3)
Hazard ratio (95% CI) | 0.58 (0.43, 0.77) | 0.59 (0.45, 0.78) | ---
p-Value (stratified log-rank) | <0.001 | <0.001 | ---
Objective Response Rate
ORR [All responses were partial responses] (95% CI) | 30% (23, 39) | 29% (22, 37) | 8% (4, 13)
p-Value (Miettinen-Nurminen) | <0.001 | <0.001 | ---
Median duration of response in months (range) | NR (0.7+, 16.8+) | NR (2.1+, 17.8+) | 8.1 (2.1+, 8.8+)
NR = not reached

Table 66: Efficacy Results of All Randomized Patients (TPS ≥1%) in KEYNOTE-010
Endpoint | Intravenous Pembrolizumab 2 mg/kg every 3 weeks n=344 | Intravenous Pembrolizumab 10 mg/kg every 3 weeks n=346 | Docetaxel 75 mg/m^2 every 3 weeks n=343
OS
Deaths (%) | 172 (50%) | 156 (45%) | 193 (56%)
Median in months (95% CI) | 10.4 (9.4, 11.9) | 12.7 (10.0, 17.3) | 8.5 (7.5, 9.8)
Hazard ratio [Hazard ratio (intravenous pembrolizumab compared to docetaxel) based on the stratified Cox proportional hazard model] (95% CI) | 0.71 (0.58, 0.88) | 0.61 (0.49, 0.75) | ---
p-Value (stratified log-rank) | <0.001 | <0.001 | ---
PFS
Events (%) | 266 (77%) | 255 (74%) | 257 (75%)
Median in months (95% CI) | 3.9 (3.1, 4.1) | 4.0 (2.6, 4.3) | 4.0 (3.1, 4.2)
Hazard ratio (95% CI) | 0.88 (0.73, 1.04) | 0.79 (0.66, 0.94) | ---
p-Value (stratified log-rank) | 0.068 | 0.005 | ---
Objective Response Rate
ORR [All responses were partial responses] (95% CI) | 18% (14, 23) | 19% (15, 23) | 9% (7, 13)
p-Value (Miettinen-Nurminen) | <0.001 | <0.001 | ---
Median duration of response in months (range) | NR (0.7+, 20.1+) | NR (2.1+, 17.8+) | 6.2 (1.4+, 8.8+)
NR = not reached

Figure 9: Kaplan-Meier Curve for Overall Survival in all Randomized Patients in KEYNOTE-010 (TPS ≥1%)

Neoadjuvant and adjuvant treatment of resectable NSCLC

The efficacy of intravenous pembrolizumab in combination with neoadjuvant chemotherapy followed by surgery and continued adjuvant treatment with intravenous pembrolizumab as a single agent was investigated in KEYNOTE-671 (NCT03425643), a multicenter, randomized, double-blind, placebo-controlled trial conducted in 797 patients with previously untreated and resectable Stage II, IIIA, or IIIB (N2) NSCLC by AJCC 8th edition. Patients were enrolled regardless of tumor PD-L1 expression. Patients with active autoimmune disease that required systemic therapy within 2 years of treatment, a medical condition that required immunosuppression, or a history of interstitial lung disease or pneumonitis that required steroids were ineligible. Randomization was stratified by stage (II vs. III), tumor PD-L1 expression (TPS ≥50% or <50%), histology (squamous vs. nonsquamous), and geographic region (East Asia vs. non-East Asia).

Patients were randomized (1:1) to one of the following treatment arms:

- Treatment Arm A: neoadjuvant intravenous pembrolizumab 200 mg on Day 1 in combination with cisplatin 75 mg/m^2 and either pemetrexed 500 mg/m^2 on Day 1 or gemcitabine 1000 mg/m^2 on Days 1 and 8 of each 21-day cycle for up to 4 cycles. Within 4-12 weeks following surgery, intravenous pembrolizumab 200 mg was administered every 3 weeks for up to 13 cycles.
- Treatment Arm B: neoadjuvant placebo on Day 1 in combination with cisplatin 75 mg/m^2 and either pemetrexed 500 mg/m^2 on Day 1 or gemcitabine 1000 mg/m^2 on Days 1 and 8 of each 21-day cycle for up to 4 cycles. Within 4-12 weeks following surgery, placebo was administered every 3 weeks for up to 13 cycles.

All study medications were administered via intravenous infusion. Treatment with intravenous pembrolizumab or placebo continued until completion of the treatment (17 cycles), disease progression that precluded definitive surgery, disease recurrence in the adjuvant phase, disease progression for those who did not undergo surgery or had incomplete resection and entered the adjuvant phase, or unacceptable toxicity. Assessment of tumor status was performed at baseline, Week 7, and Week 13 in the neoadjuvant phase and within 4 weeks prior to the start of the adjuvant phase. Following the start of the adjuvant phase, assessment of tumor status was performed every 16 weeks through the end of Year 3, and then every 6 months thereafter.

The trial was not designed to isolate the effect of intravenous pembrolizumab in each phase (neoadjuvant or adjuvant) of treatment.

The major efficacy outcome measures were OS and investigator-assessed event-free survival (EFS). Additional efficacy outcome measures were pathological complete response (pCR) rate and major pathological response (mPR) rate as assessed by blinded independent pathology review.

The study population characteristics were: median age of 64 years (range: 26 to 83); 45% age 65 or older and 7% age 75 or older; 71% male; 61% White, 31% Asian, 2% Black, 4% race not reported; 9% Hispanic or Latino; 63% ECOG PS of 0 and 37% ECOG PS of 1. Thirty percent had Stage II and 70% had Stage III disease; 33% had TPS ≥50% and 67% had TPS <50%; 43% had tumors with squamous histology and 57% had tumors with non-squamous histology; 31% were from the East Asian region.

Eighty-one percent of patients in the intravenous pembrolizumab in combination with platinum-containing chemotherapy arm received definitive surgery compared to 76% of patients in the placebo in combination with platinum-containing chemotherapy arm.

The trial demonstrated statistically significant improvements in OS and EFS for patients randomized to intravenous pembrolizumab in combination with platinum-containing chemotherapy followed by intravenous pembrolizumab as a single agent compared with patients randomized to placebo in combination with platinum-containing chemotherapy followed by placebo alone.

Table 67 and Figure 10 summarize the efficacy results for KEYNOTE-671.

Table 67: Efficacy Results in KEYNOTE-671
Endpoint | Intravenous Pembrolizumab 200 mg every 3 weeks with chemotherapy/Intravenous Pembrolizumab n=397 | Placebo with chemotherapy/Placebo n=400
OS
Number of patients with event (%) | 110 (28%) | 144 (36%)
Median in months [Based on Kaplan-Meier estimates] (95% CI) | NR (NR, NR) | 52.4 (45.7, NR)
Hazard ratio [Based on Cox regression model with treatment as a covariate stratified by stage, tumor PD-L1 expression, histology, and geographic region] (95% CI) | 0.72 (0.56, 0.93)
p-Value [Based on stratified log-rank test] , [Compared to a two-sided p-Value boundary of 0.0109] | 0.0103
EFS
Number of patients with event (%) | 139 (35%) | 205 (51%)
Median in months (95% CI) | NR (34.1, NR) | 17.0 (14.3, 22.0)
Hazard ratio (95% CI) | 0.58 (0.46, 0.72)
p-Value, [Compared to a two-sided p-Value boundary of 0.0092] | <0.0001
NR = not reached

Figure 10: Kaplan-Meier Curve for Overall Survival in KEYNOTE-671

The trial demonstrated a statistically significant difference in pCR rate (18.1% vs. 4.0%; p<0.0001) and mPR rate (30.2% vs. 11.0%; p<0.0001).

Adjuvant treatment of resected NSCLC

The efficacy of intravenous pembrolizumab was investigated in KEYNOTE-091 (NCT02504372), a multicenter, randomized, triple-blind, placebo-controlled trial conducted in 1177 patients with completely resected Stage IB (T2a ≥4 cm), II, or IIIA NSCLC by AJCC 7th edition. Patients had not received neoadjuvant radiotherapy or chemotherapy. Adjuvant chemotherapy up to 4 cycles was optional. Patients were ineligible if they had active autoimmune disease, were on chronic immunosuppressive agents, or had a history of interstitial lung disease or pneumonitis. Randomization was stratified by stage (IB vs. II vs. IIIA), receipt of adjuvant chemotherapy (yes vs. no), PD-L1 status (TPS <1% [negative] vs. TPS 1-49% vs. TPS ≥50%), and geographic region (Western Europe vs. Eastern Europe vs. Asia vs. Rest of World). Patients were randomized (1:1) to receive intravenous pembrolizumab 200 mg or placebo intravenously every 3 weeks.

Treatment continued until RECIST v1.1-defined disease recurrence as determined by the investigator, unacceptable toxicity or up to one year. Tumor assessments were conducted every 12 weeks for the first year, then every 6 months for years 2 to 3, and then annually through year 5. After year 5, imaging was performed as per local standard of care. The major efficacy outcome measure was investigator-assessed disease-free survival (DFS). An additional efficacy outcome measure was OS.

Of 1177 patients randomized, 1010 (86%) received adjuvant platinum-based chemotherapy following resection. Among these 1010 patients, the median age was 64 years (range: 35 to 84), 49% age 65 or older; 68% male; 77% White, 18% Asian; 86% current or former smokers; and 39% with ECOG PS of 1. Eleven percent had Stage IB, 57% had Stage II, and 31% had Stage IIIA disease. Thirty-nine percent had PD-L1 TPS <1% [negative], 33% had TPS 1-49%, and 28% had TPS ≥50%. Fifty-two percent were from Western Europe, 20% from Eastern Europe, 17% from Asia, and 11% from Rest of World.

The trial met its primary endpoint, demonstrating a statistically significant improvement in DFS in the overall population for patients randomized to the intravenous pembrolizumab arm compared to patients randomized to the placebo arm. In an exploratory subgroup analysis of the 167 patients (14%) who did not receive adjuvant chemotherapy, the DFS HR was 1.25 (95% CI: 0.76, 2.05). OS results were not mature with only 42% of pre-specified OS events in the overall population.

Table 68 and Figure 11 summarize the efficacy results for KEYNOTE-091 in patients who received adjuvant chemotherapy.

Table 68: Efficacy Results in KEYNOTE-091 for Patients Who Received Adjuvant Chemotherapy
Endpoint | Intravenous Pembrolizumab 200 mg every 3 weeks n=506 | Placebo n=504
DFS
Number (%) of patients with event | 177 (35%) | 231 (46%)
Median in months (95% CI) | 58.7 (39.2, NR) | 34.9 (28.6, NR)
Hazard ratio [Based on the unstratified univariate Cox regression model] (95% CI) | 0.73 (0.60, 0.89)
NR = not reached

Figure 11: Kaplan-Meier Curve for Disease-Free Survival in KEYNOTE-091 for Patients Who Received Adjuvant Chemotherapy

14.4 Malignant Pleural Mesothelioma

First-line treatment of unresectable advanced or metastatic malignant pleural mesothelioma (MPM) with pemetrexed and platinum chemotherapy

The efficacy of intravenous pembrolizumab in combination with pemetrexed and platinum chemotherapy was investigated in KEYNOTE-483 (NCT02784171), a multicenter, randomized, open-label, active-controlled trial that enrolled 440 patients with unresectable advanced or metastatic MPM and no prior systemic therapy for advanced/metastatic disease. Patients were enrolled regardless of tumor PD-L1 expression. Patients with autoimmune disease that required systemic therapy within 3 years of treatment or a medical condition that required immunosuppression were ineligible. Randomization was stratified by histological subtype (epithelioid vs. non-epithelioid). Patients were randomized (1:1) to one of the following treatment arms; all study medications were administered via intravenous infusion:

- Intravenous pembrolizumab 200 mg with pemetrexed 500 mg/m^2 and cisplatin 75 mg/m^2 or carboplatin AUC 5-6 mg/mL/min on Day 1 of each 21-day cycle for up to 6 cycles, followed by intravenous pembrolizumab 200 mg every 3 weeks.
- Pemetrexed 500 mg/m^2 and cisplatin 75 mg/m^2 or carboplatin AUC 5-6 mg/mL/min on Day 1 of each 21-day cycle for up to 6 cycles.

Treatment with intravenous pembrolizumab continued until disease progression as determined by the investigator according to modified RECIST 1.1 for mesothelioma (mRECIST), unacceptable toxicity, or a maximum of 24 months. Assessment of tumor status was performed every 6 weeks for 18 weeks, followed by every 12 weeks thereafter. The main efficacy outcome measure was OS. Additional efficacy outcome measures were PFS, ORR, and DoR, as assessed by BICR according to mRECIST.

The study population characteristics were: median age of 70 years (77% age 65 or older); 76% male; 79% White, 21% race not reported or unknown; 2% Hispanic or Latino; and 53% ECOG performance status of 1. Seventy-eight percent had epithelioid and 22% had non-epithelioid histology; 60% had tumors with PD-L1 CPS ≥1 and 30% had tumors with PD-L1 CPS <1.

The trial demonstrated a statistically significant improvement in OS, PFS, and ORR in patients randomized to intravenous pembrolizumab in combination with chemotherapy compared with patients randomized to chemotherapy alone. Table 69 and Figure 12 summarize the efficacy results for KEYNOTE-483.

Table 69: Efficacy Results in KEYNOTE-483
Endpoint | Intravenous pembrolizumab 200 mg every 3 weeks Pemetrexed Platinum Chemotherapy | Pemetrexed Platinum Chemotherapy
 | (n=222) | (n=218)
OS
Number (%) of patients with event | 167 (75%) | 175 (80%)
Median in months (95% CI) | 17.3 (14.4, 21.3) | 16.1 (13.1, 18.2)
Hazard ratio [Based on stratified Cox proportional hazard model] (95% CI) | 0.79 (0.64, 0.98)
p-Value [Based on stratified log-rank test] | 0.0162
PFS
Number (%) of patients with event | 190 (86%) | 166 (76%)
Median in months (95% CI) | 7.1 (6.9, 8.1) | 7.1 (6.8, 7.7)
Hazard ratio (95% CI) | 0.80 (0.65, 0.99)
p-Value | 0.0194
Objective Response Rate
ORR % (95% CI) | 52% (45.5, 59.0) | 29% (23.0, 35.4)
Complete responses | 1 (0.5%) | 0 (0%)
Partial responses | 115 (52%) | 63 (29%)
p-Value [Based on Miettinen and Nurminen method stratified by histological subtype at randomization (epithelioid vs. non-epithelioid)] | <0.00001
Duration of Response [Based on patients with a best overall response as confirmed complete or partial response; n=116 for patients in the intravenous pembrolizumab combination arm; n=63 for patients in the chemotherapy arm]
Median in months (95% CI) | 6.9 (5.8, 8.3) | 6.8 (5.5, 8.5)

Figure 12: Kaplan-Meier Curve for Overall Survival in KEYNOTE-483

In a pre-specified exploratory analysis based on histology, in the subgroup of patients with epithelioid histology (n=345), the hazard ratio (HR) for OS was 0.89 (95% CI: 0.70, 1.13), with median OS of 19.8 months in intravenous pembrolizumab in combination with chemotherapy and 18.2 months in chemotherapy alone. In the subgroup of patients with non-epithelioid histology (n=95), the HR for OS was 0.57 (95% CI: 0.36, 0.89), with median OS of 12.3 months in intravenous pembrolizumab in combination with chemotherapy and 8.2 months in chemotherapy alone.

14.5 Head and Neck Squamous Cell Cancer

Neoadjuvant and Adjuvant Treatment of Locally Advanced HNSCC for Tumors Expressing PD-L1 (CPS ≥1)

The efficacy of intravenous pembrolizumab was investigated in KEYNOTE-689 (NCT02358031), a randomized, multicenter, open-label, active-controlled trial conducted in 714 patients with resectable locally advanced (Stage III-IVA) HNSCC [AJCC, 8th edition]. Patients with active autoimmune disease requiring systemic therapy within two years of treatment or a medical condition that required immunosuppression were ineligible. Randomization was stratified by primary tumor site (oropharynx/oral cavity vs. larynx vs. hypopharynx), tumor stage (III vs. IVA) and PD-L1 status (TPS ≥ 50% vs. TPS<50%) according to the PD-L1 IHC 22C3 pharmDx assay.

Patients were randomized (1:1) to one of the following treatment arms:

- neoadjuvant intravenous pembrolizumab 200 mg for 2 cycles prior to surgical resection. Within 6 weeks following surgery, 3 cycles of adjuvant intravenous pembrolizumab 200 mg every 3 weeks in combination with radiotherapy (RT) with or without 3 cycles of cisplatin 100 mg/m^2 every 3 weeks. This was followed by intravenous pembrolizumab 200 mg every 3 weeks for up to 12 cycles.
- no neoadjuvant treatment prior to surgery. Within 6 weeks following surgery, adjuvant RT with or without 3 cycles of concurrent cisplatin 100 mg/m^2 every 3 weeks.
  On both treatment arms, patients received cisplatin with adjuvant RT if high-risk pathological features (i.e., positive margins <1 mm or extranodal extension) were present at surgery.

Treatment with intravenous pembrolizumab continued until disease progression by RECIST v1.1 per BICR during the neoadjuvant phase that precluded surgery, local or metastatic recurrence during the adjuvant phase, completion of treatment, or unacceptable toxicity. Assessment of tumor status was performed prior to surgery at Week 6 in the neoadjuvant phase. Following the start of the adjuvant phase, assessment of tumor status was performed 12 weeks after end of RT with or without cisplatin treatment and then every 3 months until the end of year 3; then every 6 months thereafter up to the end of year 5.

The trial was not designed to isolate the effect of intravenous pembrolizumab in each phase (neoadjuvant or adjuvant) of treatment.

The major efficacy outcome measure was event-free survival (EFS) by BICR defined as the time from randomization to the first occurrence of any of the following events: progression of disease that precludes definitive surgery, local or distant disease progression or recurrence, or death due to any cause. Additional efficacy outcome measures were major pathological response (mPR) as assessed by BIPR, and overall survival (OS).

The demographic and baseline characteristics in the 682 patients with PD-L1 expression of CPS ≥1 were: median age of 60 years (range: 22 to 87), 33% age 65 or older; 79% male; 78% White, 13% Asian and 2.5% Black or African American, 14% were Hispanic or Latino; 43% had ECOG PS of 1, and 79% were former/current smokers. Four percent of patients’ tumors were HPV-positive, and 26% had Stage III disease, 74% had Stage IVA disease. Sixty-eight percent of patients’ tumors had PD-L1 expression of CPS ≥10.

Eighty-eight percent of patients received definitive surgery in both the intravenous pembrolizumab and the SOC arm.

Seventy-six percent of patients in the intravenous pembrolizumab arm and 78% of patients in the SOC arm started the radiation phase of treatment. In the intravenous pembrolizumab arm, 35% of patients received intravenous pembrolizumab and cisplatin with concurrent RT, 57% of patients received intravenous pembrolizumab alone with concurrent RT, 3% of patients received cisplatin alone with concurrent RT, 5% of patients received RT alone and one patient (0.4%) received intravenous pembrolizumab alone without concurrent RT. On the SoC arm, 52% of patients received cisplatin with concurrent RT while 48% patients received RT alone.

The trial demonstrated a statistically significant improvement in EFS for patients randomized to the intravenous pembrolizumab arm compared to those randomized to the standard of care (SOC) arm at the first pre-specified interim analysis. Table 70 and Figure 13 summarize efficacy results in KEYNOTE-689 for patients with HNSCC CPS ≥1.

Table 70: Efficacy Results for Perioperative Intravenous Pembrolizumab with adjuvant RT with or without cisplatin in Patients with HNSCC CPS ≥1 in KEYNOTE-689
Endpoint | Intravenous Pembrolizumab 200 mg every 3 weeks with RT with or without cisplatin n=347 | RT with or without cisplatin n=335
EFS
Number of events, n (%) | 128 (37%) | 156 (47%)
Median in months [From product-limit (Kaplan-Meier) method for censored data.] (95% CI) | 59.7 (37.9, NR) | 29.6 (19.5, 41.9)
Hazard ratio [Based on Cox regression model with Efron’s method of tie handling with treatment as a covariate stratified by primary tumor site and tumor stage.] (95% CI) | 0.70 (0.55, 0.89)
p-Value [One-sided p-value based on log-rank test stratified by primary tumor site and tumor stage. Compared to a one-sided p-value boundary of 0.0124] , | 0.00140
NR = not reached

Figure 13: Kaplan-Meier Curve for Event-free Survival for Intravenous Pembrolizumab in Patients with HNSCC CPS ≥1 in KEYNOTE-689

While OS results were not mature at this interim analysis, with 76% of pre-specified OS events in the CPS ≥1 population, no trend towards a detriment was observed.

Hypopharyngeal Tumors

In an exploratory subgroup analysis of patients with PD-L1-positive (CPS ≥1) hypopharyngeal tumors who were randomized (n=51), the EFS HR was 2.28 (95% CI: 0.79, 6.56). Among these patients, 23 patients in the intravenous pembrolizumab arm received surgery, of which 17 patients (74%) had R0 resections. On the SOC arm, 23 patients received surgery, of which 20 (87%) had R0 resections.

Oral Cavity, Oropharyngeal and Laryngeal Tumors

In an exploratory subgroup analysis of patients with PD-L1 positive (CPS ≥1) oral cavity, oropharyngeal and laryngeal tumors who received surgery (n=555), 91% of patients on the intravenous pembrolizumab arm had R0 resections while 85% of patients on the SOC arm had R0 resections.

First-line treatment of metastatic or unresectable, recurrent HNSCC

The efficacy of intravenous pembrolizumab was investigated in KEYNOTE-048 (NCT02358031), a randomized, multicenter, open-label, active-controlled trial conducted in 882 patients with metastatic HNSCC who had not previously received systemic therapy for metastatic disease or with recurrent disease who were considered incurable by local therapies. Patients with active autoimmune disease that required systemic therapy within two years of treatment or a medical condition that required immunosuppression were ineligible. Randomization was stratified by tumor PD-L1 expression (TPS ≥50% or <50%) according to the PD-L1 IHC 22C3 pharmDx assay, HPV status according to p16 IHC (positive or negative), and ECOG PS (0 vs. 1). Patients were randomized 1:1:1 to one of the following treatment arms:

- Intravenous pembrolizumab 200 mg intravenously every 3 weeks
- Intravenous pembrolizumab 200 mg intravenously every 3 weeks, carboplatin AUC 5 mg/mL/min intravenously every 3 weeks or cisplatin 100 mg/m^2 intravenously every 3 weeks, and FU 1000 mg/m^2/day as a continuous intravenous infusion over 96 hours every 3 weeks (maximum of 6 cycles of platinum and FU)
- Cetuximab 400 mg/m^2 intravenously as the initial dose then 250 mg/m^2 intravenously once weekly, carboplatin AUC 5 mg/mL/min intravenously every 3 weeks or cisplatin 100 mg/m^2 intravenously every 3 weeks, and FU 1000 mg/m^2/day as a continuous intravenous infusion over 96 hours every 3 weeks (maximum of 6 cycles of platinum and FU)

Treatment with intravenous pembrolizumab continued until RECIST v1.1-defined progression of disease as determined by the investigator, unacceptable toxicity, or a maximum of 24 months. Administration of intravenous pembrolizumab was permitted beyond RECIST-defined disease progression if the patient was clinically stable and considered to be deriving clinical benefit by the investigator. Assessment of tumor status was performed at Week 9 and then every 6 weeks for the first year, followed by every 9 weeks through 24 months. A retrospective re-classification of patients' tumor PD-L1 status according to CPS using the PD-L1 IHC 22C3 pharmDx assay was conducted using the tumor specimens used for randomization.

The main efficacy outcome measures were OS and PFS as assessed by BICR according to RECIST v1.1 (modified to follow a maximum of 10 target lesions and a maximum of 5 target lesions per organ) sequentially tested in the subgroup of patients with CPS ≥20, the subgroup of patients with CPS ≥1, and the overall population.

The study population characteristics were: median age of 61 years (range: 20 to 94), 36% age 65 or older; 83% male; 73% White, 20% Asian and 2.4% Black; 61% had ECOG PS of 1; and 79% were former/current smokers. Twenty-two percent of patients' tumors were HPV-positive, 23% had PD-L1 TPS ≥50%, and 95% had Stage IV disease (Stage IVA 19%, Stage IVB 6%, and Stage IVC 70%). Eighty-five percent of patients' tumors had PD-L1 expression of CPS ≥1 and 43% had CPS ≥20.

The trial demonstrated a statistically significant improvement in OS for patients randomized to intravenous pembrolizumab in combination with chemotherapy compared to those randomized to cetuximab in combination with chemotherapy at a pre-specified interim analysis in the overall population. Table 71 and Figure 14 summarize efficacy results for intravenous pembrolizumab in combination with chemotherapy.

Table 71: Efficacy Results [Results at a pre-specified interim analysis] for Intravenous Pembrolizumab plus Platinum/Fluorouracil in KEYNOTE-048
Endpoint | Intravenous Pembrolizumab 200 mg every 3 weeks Platinum FU | Cetuximab Platinum FU
 | n=281 | n=278
OS
Number (%) of patients with event | 197 (70%) | 223 (80%)
Median in months (95% CI) | 13.0 (10.9, 14.7) | 10.7 (9.3, 11.7)
Hazard ratio [Based on the stratified Cox proportional hazard model] (95% CI) | 0.77 (0.63, 0.93)
p-Value [Based on stratified log-rank test] | 0.0067
PFS
Number of patients with event (%) | 244 (87%) | 253 (91%)
Median in months (95% CI) | 4.9 (4.7, 6.0) | 5.1 (4.9, 6.0)
Hazard ratio (95% CI) | 0.92 (0.77, 1.10)
p-Value | 0.3394
Objective Response Rate
ORR [Response: Best objective response as confirmed complete response or partial response] (95% CI) | 36% (30.0, 41.5) | 36% (30.7, 42.3)
Complete response rate | 6% | 3%
Partial response rate | 30% | 33%
Duration of Response
Median in months (range) | 6.7 (1.6+, 30.4+) | 4.3 (1.2+, 27.9+)

At the pre-specified final OS analysis for the ITT population, the hazard ratio was 0.72 (95% CI: 0.60, 0.87). In addition, KEYNOTE-048 demonstrated a statistically significant improvement in OS for the subgroups of patients with PD-L1 CPS ≥1 (HR=0.65, 95% CI: 0.53, 0.80) and CPS ≥20 (HR=0.60, 95% CI: 0.45, 0.82).

Figure 14: Kaplan-Meier Curve for Overall Survival for Intravenous Pembrolizumab plus Platinum/Fluorouracil in KEYNOTE-048 [At the time of the protocol-specified final analysis.]

First-line treatment of metastatic or unresectable, recurrent HNSCC for Tumors Expressing PD-L1 (CPS ≥1) as a single agent

The trial also demonstrated a statistically significant improvement in OS for the subgroup of patients with PD-L1 CPS ≥1 randomized to intravenous pembrolizumab as a single agent compared to those randomized to cetuximab in combination with chemotherapy at a pre-specified interim analysis. At the time of the interim and final analyses, there was no significant difference in OS between the intravenous pembrolizumab single agent arm and the control arm for the overall population.

Table 72 summarizes efficacy results for intravenous pembrolizumab as a single agent in the subgroups of patients with CPS ≥1 HNSCC and CPS ≥20 HNSCC. Figure 15 summarizes the OS results in the subgroup of patients with CPS ≥1 HNSCC.

Table 72: Efficacy Results [Results at a pre-specified interim analysis] for Intravenous Pembrolizumab as a Single Agent in KEYNOTE-048 (CPS ≥1 and CPS ≥20)
Endpoint | CPS ≥1 |  | CPS ≥20
Endpoint | Intravenous Pembrolizumab 200 mg every 3 weeks | Cetuximab Platinum FU | Intravenous Pembrolizumab 200 mg every 3 weeks | Cetuximab Platinum FU
Endpoint | n=257 | n=255 | n=133 | n=122
OS
Number of events (%) | 177 (69%) | 206 (81%) | 82 (62%) | 95 (78%)
Median in months (95% CI) | 12.3 (10.8, 14.9) | 10.3 (9.0, 11.5) | 14.9 (11.6, 21.5) | 10.7 (8.8, 12.8)
Hazard ratio [Based on the stratified Cox proportional hazard model] (95% CI) | 0.78 (0.64, 0.96) |  | 0.61 (0.45, 0.83)
p-Value [Based on a stratified log-rank test] | 0.0171 |  | 0.0015
PFS
Number of events (%) | 225 (88%) | 231 (91%) | 113 (85%) | 111 (91%)
Median in months (95% CI) | 3.2 (2.2, 3.4) | 5.0 (4.8, 5.8) | 3.4 (3.2, 3.8) | 5.0 (4.8, 6.2)
Hazard ratio (95% CI) | 1.15 (0.95, 1.38) |  | 0.97 (0.74, 1.27)
Objective Response Rate
ORR [Response: Best objective response as confirmed complete response or partial response] (95% CI) | 19% (14.5, 24.4) | 35% (29.1, 41.1) | 23% (16.4, 31.4) | 36% (27.6, 45.3)
Complete response rate | 5% | 3% | 8% | 3%
Partial response rate | 14% | 32% | 16% | 33%
Duration of Response
Median in months (range) | 20.9 (1.5+, 34.8+) | 4.5 (1.2+, 28.6+) | 20.9 (2.7, 34.8+) | 4.2 (1.2+, 22.3+)

At the pre-specified final OS analysis comparing intravenous pembrolizumab as a single agent to cetuximab in combination with chemotherapy, the hazard ratio for the subgroup of patients with CPS ≥1 was 0.74 (95% CI: 0.61, 0.90) and the hazard ratio for the subgroup of patients with CPS ≥20 was 0.58 (95% CI: 0.44, 0.78).

In an exploratory subgroup analysis for patients with CPS 1-19 HNSCC at the time of the pre-specified final OS analysis, the median OS was 10.8 months (95% CI: 9.0, 12.6) for intravenous pembrolizumab as a single agent and 10.1 months (95% CI: 8.7, 12.1) for cetuximab in combination with chemotherapy, with an HR of 0.86 (95% CI: 0.66, 1.12).

Figure 15: Kaplan-Meier Curve for Overall Survival for Intravenous Pembrolizumab as a Single Agent in KEYNOTE-048 (CPS ≥1) [At the time of the protocol-specified final analysis.]

Previously treated recurrent or metastatic HNSCC

The efficacy of intravenous pembrolizumab was investigated in KEYNOTE-012 (NCT01848834), a multicenter, non-randomized, open-label, multi-cohort study that enrolled 174 patients with recurrent or metastatic HNSCC who had disease progression on or after platinum-containing chemotherapy administered for recurrent or metastatic HNSCC or following platinum-containing chemotherapy administered as part of induction, concurrent, or adjuvant therapy. Patients with active autoimmune disease, a medical condition that required immunosuppression, evidence of interstitial lung disease, or ECOG PS ≥2 were ineligible.

Patients received intravenous pembrolizumab 10 mg/kg every 2 weeks (n=53) or 200 mg every 3 weeks (n=121) until unacceptable toxicity or disease progression that was symptomatic, was rapidly progressive, required urgent intervention, occurred with a decline in performance status, or was confirmed at least 4 weeks later with repeat imaging. Patients without disease progression were treated for up to 24 months. Treatment with pembrolizumab could be reinitiated for subsequent disease progression and administered for up to 1 additional year. Assessment of tumor status was performed every 8 weeks. The major efficacy outcome measures were ORR according to RECIST v1.1, modified to follow a maximum of 10 target lesions and a maximum of 5 target lesions per organ, as assessed by BICR, and DoR.

The study population characteristics were median age of 60 years, 32% age 65 or older; 82% male; 75% White, 16% Asian, and 6% Black; 87% had M1 disease; 33% had HPV positive tumors; 63% had prior cetuximab; 29% had an ECOG PS of 0 and 71% had an ECOG PS of 1; and the median number of prior lines of therapy administered for the treatment of HNSCC was 2.

The ORR was 16% (95% CI: 11, 22) with a complete response rate of 5%. The median follow-up time was 8.9 months. Among the 28 responding patients, the median DoR had not been reached (range: 2.4+ to 27.7+ months), with 23 patients having responses of 6 months or longer. The ORR and DoR were similar irrespective of dosage regimen (10 mg/kg every 2 weeks or 200 mg every 3 weeks) or HPV status.

14.6 Urothelial Cancer

In Combination with Enfortumab Vedotin for the Treatment of Patients with Urothelial Cancer

The efficacy of intravenous pembrolizumab in combination with enfortumab vedotin was evaluated in KEYNOTE-A39 (NCT04223856), an open-label, randomized, multicenter trial that enrolled 886 patients with locally advanced or metastatic urothelial cancer who received no prior systemic therapy for locally advanced or metastatic disease. Patients with active CNS metastases, ongoing sensory or motor neuropathy Grade ≥2, or uncontrolled diabetes defined as hemoglobin A1C (HbA1c) ≥8% or HbA1c ≥7% with associated diabetes symptoms were excluded.

Patients were randomized 1:1 to receive either:

- Intravenous pembrolizumab 200 mg over 30 minutes on Day 1 and enfortumab vedotin 1.25 mg/kg on Days 1 and 8 of each 21-day cycle. Intravenous pembrolizumab was given approximately 30 minutes after enfortumab vedotin. Treatment was continued until disease progression or unacceptable toxicity. In the absence of disease progression or unacceptable toxicity, intravenous pembrolizumab was continued for up to 2 years.
- Gemcitabine 1000 mg/m^2 on Days 1 and 8 of a 21-day cycle with cisplatin 70 mg/m^2 or carboplatin (AUC = 4.5 or 5) on Day 1 of a 21-day cycle. Treatment was continued until disease progression or unacceptable toxicity for up to 6 cycles.

Randomization was stratified by cisplatin eligibility, PD-L1 expression, and presence of liver metastases.

The median age was 69 years (range: 22 to 91); 77% were male; 67% were White, 22% were Asian, 1% were Black or African American, and 10% were unknown or other; 12% were Hispanic or Latino. Patients had a baseline ECOG performance status of 0 (49%), 1 (47%), or 2 (3%). Forty-seven percent of patients had a documented baseline HbA1c of <5.7%. At baseline, 95% of patients had metastatic urothelial cancer, including 72% with visceral and 22% with liver metastases, and 5% had locally advanced urothelial cancer. Eighty-five percent of patients had urothelial carcinoma (UC) histology including 6% with UC mixed squamous differentiation and 2% with UC mixed other histologic variants. Forty-six percent of patients were considered cisplatin-ineligible and 54% were considered cisplatin-eligible at time of randomization.

The major efficacy outcome measures were OS and PFS as assessed by BICR according to RECIST v1.1. Additional efficacy outcome measures included ORR as assessed by BICR.

The trial demonstrated statistically significant improvements in OS, PFS, and ORR for patients randomized to intravenous pembrolizumab in combination with enfortumab vedotin as compared to platinum-based chemotherapy. Efficacy results were consistent across all stratified patient subgroups.

Table 73 and Figures 16 and 17 summarize the efficacy results for KEYNOTE-A39.

Table 73: Efficacy Results in KEYNOTE-A39
Endpoint | Intravenous Pembrolizumab 200 mg every 3 weeks in combination with Enfortumab Vedotin n=442 | Cisplatin or Carboplatin with Gemcitabine n=444
OS
Number (%) of patients with event | 133 (30%) | 226 (51%)
Median in months (95% CI) | 31.5 (25.4, NR) | 16.1 (13.9, 18.3)
Hazard ratio [Based on the stratified Cox proportional hazard regression model] (95% CI) | 0.47 (0.38, 0.58)
p-Value [Two-sided p-Value based on stratified log-rank test] | <0.0001
PFS
Number (%) of patients with event | 223 (50%) | 307 (69%)
Median in months (95% CI) | 12.5 (10.4, 16.6) | 6.3 (6.2, 6.5)
Hazard ratio (95% CI) | 0.45 (0.38, 0.54)
p-Value | <0.0001
Confirmed Objective Response Rate [Includes only patients with measurable disease at baseline (n=437 for intravenous pembrolizumab in combination with enfortumab vedotin, n=441 for chemotherapy).]
ORR [Based on patients with a best overall response as confirmed complete or partial response] % (95% CI) | 68% (63, 72) | 44% (40, 49)
p-Value [Two-sided p-Value based on Cochran-Mantel-Haenszel test stratified by PD-L1 expression, cisplatin eligibility and liver metastases] | <0.0001
Complete response | 29% | 12%
Partial response | 39% | 32%
NR = not reached

Figure 16: Kaplan-Meier Curve for Overall Survival in KEYNOTE-A39

Figure 17: Kaplan-Meier Curve for Progression-Free Survival in KEYNOTE-A39

In Combination with Enfortumab Vedotin for the Treatment of Cisplatin-Ineligible Patients with Urothelial Cancer

The efficacy of intravenous pembrolizumab in combination with enfortumab vedotin was evaluated in KEYNOTE-869 (NCT03288545), an open-label, multi-cohort (dose escalation cohort, Cohort A, Cohort K) study in patients with locally advanced or metastatic urothelial cancer who were ineligible for cisplatin-containing chemotherapy and received no prior systemic therapy for locally advanced or metastatic disease. Patients with active CNS metastases, ongoing sensory or motor neuropathy Grade ≥2, or uncontrolled diabetes defined as hemoglobin A1C (HbA1c) ≥8% or HbA1c ≥7% with associated diabetes symptoms were excluded from participating in the study.

Patients in the dose escalation cohort (n=5), Cohort A (n=40), and Cohort K (n=76) received enfortumab vedotin 1.25 mg/kg as an IV infusion over 30 minutes on Days 1 and 8 of a 21-day cycle followed by intravenous pembrolizumab 200 mg as an IV infusion on Day 1 of a 21-day cycle approximately 30 minutes after enfortumab vedotin. Patients were treated until disease progression or unacceptable toxicity.

A total of 121 patients received intravenous pembrolizumab in combination with enfortumab vedotin. The median age was 71 years (range: 51 to 91); 74% were male; 85% were White, 5% were Black, 4% were Asian and 6% were other, unknown or not reported. Ten percent of patients were Hispanic or Latino. Forty-five percent of patients had an ECOG performance status of 1 and 15% had an ECOG performance status of 2. Forty-seven percent of patients had a documented baseline HbA1c of <5.7%. Reasons for cisplatin-ineligibility included: 60% with baseline creatinine clearance of 30-59 mL/min, 10% with ECOG PS of 2, 13% with Grade 2 or greater hearing loss, and 16% with more than one cisplatin-ineligibility criteria.

At baseline, 97.5% of patients had metastatic urothelial cancer and 2.5% of patients had locally advanced urothelial cancer. Thirty-seven percent of patients had upper tract disease. Eighty-four percent of patients had visceral metastasis at baseline, including 22% with liver metastases. Thirty-nine percent of patients had TCC histology; 13% had TCC with squamous differentiation, and 48% had TCC with other histologic variants.

The major efficacy outcome measures were ORR and DoR as assessed by BICR according to RECIST v1.1.

The median follow-up time for the dose escalation cohort + Cohort A was 44.7 months (range 0.7 to 52.4) and for Cohort K was 14.8 months (range: 0.6 to 26.2).

Efficacy results are presented in Table 74 below.

Table 74: Efficacy Results in KEYNOTE-869, Combined Dose Escalation Cohort, Cohort A, and Cohort K
Endpoint | Intravenous Pembrolizumab in combination with Enfortumab Vedotin n=121
Confirmed ORR (95% CI) | 68% (58.7, 76.0)
Complete response rate | 12%
Partial response rate | 55%

The median duration of response for the dose escalation cohort + Cohort A was 22.1 months (range: 1.0+ to 46.3+) and for Cohort K was not reached (range: 1.2 to 24.1+).

Platinum-Ineligible Patients with Urothelial Carcinoma

The efficacy of intravenous pembrolizumab was investigated in KEYNOTE-052 (NCT02335424), a multicenter, open-label, single-arm trial in 370 patients with locally advanced or metastatic urothelial carcinoma who had one or more comorbidities, including patients who were not eligible for any platinum-containing chemotherapy. The trial excluded patients with autoimmune disease or a medical condition that required immunosuppression. Patients received intravenous pembrolizumab 200 mg every 3 weeks until unacceptable toxicity or disease progression. Patients with initial radiographic disease progression could receive additional doses of treatment during confirmation of progression unless disease progression was symptomatic, was rapidly progressive, required urgent intervention, or occurred with a decline in performance status. Patients without disease progression could be treated for up to 24 months. Tumor response assessments were performed at 9 weeks after the first dose, then every 6 weeks for the first year, and then every 12 weeks thereafter. The major efficacy outcome measures were ORR and DoR as assessed by BICR according to RECIST v1.1, modified to follow a maximum of 10 target lesions and a maximum of 5 target lesions per organ.

The study population characteristics were: median age of 74 years; 77% male; and 89% White. Eighty-seven percent had M1 disease, and 13% had M0 disease. Eighty-one percent had a primary tumor in the lower tract, and 19% of patients had a primary tumor in the upper tract. Eighty-five percent of patients had visceral metastases, including 21% with liver metastases. Fifty percent of patients had baseline creatinine clearance of <60 mL/min, 32% had ECOG PS of 2, 9% had ECOG PS of 2 and baseline creatinine clearance of <60 mL/min, and 9% had one or more of Class III heart failure, Grade 2 or greater peripheral neuropathy, and Grade 2 or greater hearing loss. Ninety percent of patients were treatment naïve, and 10% received prior adjuvant or neoadjuvant platinum-based chemotherapy.

The median follow-up time for 370 patients treated with intravenous pembrolizumab was 11.4 months (range 0.1 to 63.8 months). Efficacy results are summarized in Table 75.

Table 75: Efficacy Results in KEYNOTE-052
Endpoint | Intravenous Pembrolizumab 200 mg every 3 weeks
 | All Subjects n=370
Objective Response Rate
ORR (95% CI) | 29% (24, 34)
Complete response rate | 10%
Partial response rate | 20%
Duration of Response
Median in months (range) | 33.4 (1.4+, 60.7+)
+ Denotes ongoing response

Platinum-Eligible Patients with Previously Untreated Urothelial Carcinoma

The efficacy of intravenous pembrolizumab for the first-line treatment of platinum-eligible patients with locally advanced or metastatic urothelial carcinoma was investigated in KEYNOTE-361 (NCT02853305), a multicenter, randomized, open-label, active-controlled study in 1010 previously untreated patients. The safety and efficacy of intravenous pembrolizumab in combination with platinum-based chemotherapy for previously untreated patients with locally advanced or metastatic urothelial carcinoma has not been established.

The study compared intravenous pembrolizumab with or without platinum-based chemotherapy (i.e., cisplatin or carboplatin with gemcitabine) to platinum-based chemotherapy alone. Among the patients receiving intravenous pembrolizumab plus platinum-based chemotherapy, 44% received cisplatin and 56% received carboplatin.

The study did not meet its major efficacy outcome measures of improved PFS or OS in the intravenous pembrolizumab plus chemotherapy arm compared to the chemotherapy-alone arm. Additional efficacy endpoints, including improvement of OS in the intravenous pembrolizumab monotherapy arm, could not be formally tested.

Previously Treated Urothelial Carcinoma

The efficacy of intravenous pembrolizumab was investigated in KEYNOTE-045 (NCT02256436), a multicenter, randomized (1:1), active-controlled trial in 542 patients with locally advanced or metastatic urothelial carcinoma with disease progression on or after platinum-containing chemotherapy. The trial excluded patients with autoimmune disease or a medical condition that required immunosuppression.

Patients were randomized to receive either intravenous pembrolizumab 200 mg every 3 weeks (n=270) or investigator's choice of any of the following chemotherapy regimens all given intravenously every 3 weeks (n=272): paclitaxel 175 mg/m^2 (n=90), docetaxel 75 mg/m^2 (n=92), or vinflunine 320 mg/m^2 (n=90). Treatment continued until unacceptable toxicity or disease progression. Patients with initial radiographic disease progression could receive additional doses of treatment during confirmation of progression unless disease progression was symptomatic, was rapidly progressive, required urgent intervention, or occurred with a decline in performance status. Patients without disease progression could be treated for up to 24 months. Assessment of tumor status was performed at 9 weeks after randomization, then every 6 weeks through the first year, followed by every 12 weeks thereafter. The major efficacy outcomes were OS and PFS as assessed by BICR per RECIST v1.1, modified to follow a maximum of 10 target lesions and a maximum of 5 target lesions per organ. Additional efficacy outcome measures were ORR as assessed by BICR per RECIST v1.1, modified to follow a maximum of 10 target lesions and a maximum of 5 target lesions per organ, and DoR.

The study population characteristics were: median age of 66 years (range: 26 to 88), 58% age 65 or older; 74% male; 72% White and 23% Asian; 42% ECOG PS of 0 and 56% ECOG PS of 1; and 96% M1 disease and 4% M0 disease. Eighty-seven percent of patients had visceral metastases, including 34% with liver metastases. Eighty-six percent had a primary tumor in the lower tract and 14% had a primary tumor in the upper tract. Fifteen percent of patients had disease progression following prior platinum-containing neoadjuvant or adjuvant chemotherapy. Twenty-one percent had received 2 or more prior systemic regimens in the metastatic setting. Seventy-six percent of patients received prior cisplatin, 23% had prior carboplatin, and 1% were treated with other platinum-based regimens.

The study demonstrated statistically significant improvements in OS and ORR for patients randomized to intravenous pembrolizumab as compared to chemotherapy. There was no statistically significant difference between intravenous pembrolizumab and chemotherapy with respect to PFS. The median follow-up time for this trial was 9.0 months (range: 0.2 to 20.8 months). Table 76 and Figure 18 summarize the efficacy results for KEYNOTE-045.

Table 76: Efficacy Results in KEYNOTE-045
 | Intravenous Pembrolizumab 200 mg every 3 weeks | Chemotherapy
 | n=270 | n=272
OS
Deaths (%) | 155 (57%) | 179 (66%)
Median in months (95% CI) | 10.3 (8.0, 11.8) | 7.4 (6.1, 8.3)
Hazard ratio [Hazard ratio (intravenous pembrolizumab compared to chemotherapy) based on the stratified Cox proportional hazard model] (95% CI) | 0.73 (0.59, 0.91)
p-Value (stratified log-rank) | 0.004
PFS by BICR
Events (%) | 218 (81%) | 219 (81%)
Median in months (95% CI) | 2.1 (2.0, 2.2) | 3.3 (2.3, 3.5)
Hazard ratio (95% CI) | 0.98 (0.81, 1.19)
p-Value (stratified log-rank) | 0.833
Objective Response Rate
ORR (95% CI) | 21% (16, 27) | 11% (8, 16)
Complete response rate | 7% | 3%
Partial response rate | 14% | 8%
p-Value (Miettinen-Nurminen) | 0.002
Median duration of response in months (range) | NR (1.6+, 15.6+) | 4.3 (1.4+, 15.4+)
+ Denotes ongoing response
NR = not reached

Figure 18: Kaplan-Meier Curve for Overall Survival in KEYNOTE-045

Neoadjuvant and Adjuvant Treatment of Cisplatin-Ineligible Patients with MIBC in Combination with Enfortumab Vedotin

The efficacy of intravenous pembrolizumab in combination with enfortumab vedotin as neoadjuvant treatment and continued after radical cystectomy as adjuvant treatment was investigated in KEYNOTE-905 (NCT03924895), an open-label, randomized, multicenter, active-controlled trial in patients with previously untreated MIBC with predominant urothelial carcinoma histology and who were candidates for radical cystectomy (RC) with pelvic lymph node dissection (PLND) but were ineligible for or declined cisplatin-based chemotherapy. The study excluded patients with primary non-bladder urothelial cancer (i.e., cancer of the ureter, urethra, or renal pelvis) and those with active autoimmune disease that required systemic therapy within 2 years of treatment or a medical condition that required immunosuppression.

Randomization was stratified by tumor stage (T2N0 vs T3/T4aN0 vs T1-T4aN1), cisplatin-eligibility (cisplatin-ineligible vs cisplatin-eligible but declined), and geographic region (United States vs European Union vs Rest of World).

Patients were randomized 1:1 to receive:

- Neoadjuvant intravenous pembrolizumab 200 mg over 30 minutes as an intravenous infusion on Day 1 and enfortumab vedotin 1.25 mg/kg as an intravenous infusion on Days 1 and 8 of each 21-day cycle for 3 cycles prior to surgery, followed by adjuvant intravenous pembrolizumab 200 mg over 30 minutes on Day 1 of each 21-day cycle for 14 cycles and adjuvant enfortumab vedotin 1.25 mg/kg on Days 1 and 8 of each 21-day cycle for 6 cycles (n=170).
- Immediate RC and PLND alone (n=174).

Treatment continued until completion of study medications, disease progression, not undergoing or refusal of RC and PLND, disease recurrence in the adjuvant phase, or unacceptable toxicity. Assessment of tumor status, including CT/MRI, was performed at baseline, within 5 weeks prior to RC and PLND, and at 6 weeks post-radical cystectomy. Following RC and PLND, assessment of tumor status, including cystoscopy and urine cytology for patients who did not undergo surgery, was performed every 12 weeks up to 2 years, and every 24 weeks thereafter.

The study population characteristics were: median age of 73 years (range: 46 to 87 years); 78% male; 78% White, 16% Asian, 3.2% Multiple, 1.2% Black or African American, 0.3% American Indian or Alaska Native, and 1.2% missing; 6% Hispanic or Latino, 91% not Hispanic or Latino, and 2.9% not reported; 57% had ECOG PS of 0, 29% had ECOG PS of 1, and 14% had ECOG PS of 2; 18% were T2N0, 77% T3/T4aN0, and 4.9% T1-T4aN1. Ninety-one percent of patients had pure urothelial carcinoma histology; 4.4% had urothelial carcinoma with squamous differentiation, 2.6% had urothelial carcinoma with glandular differentiation, and 2% had urothelial carcinoma with other variant histology. Among the 281 patients who were ineligible for cisplatin, 72% had baseline creatinine clearance of 30-59 mL/min, 17% had ECOG PS of 2, 21% had Grade 2 or greater hearing loss, 3.9% had New York Heart Association Class III heart failure, and 13% met more than one cisplatin-ineligibility criterion.

A total of 149 (88%) patients in the intravenous pembrolizumab in combination with enfortumab vedotin arm and 156 (90%) patients in the RC and PLND alone arm underwent RC and PLND.

The trial was not designed to isolate the effect of intravenous pembrolizumab in each phase (neoadjuvant or adjuvant) of treatment.

The major efficacy outcome measure was EFS as assessed by BICR. Overall survival (OS) and pathological complete response (pCR) rate as assessed by blinded independent pathology review were additional efficacy outcome measures.

The trial demonstrated a statistically significant improvement in EFS and OS in patients treated with neoadjuvant and adjuvant intravenous pembrolizumab in combination with enfortumab vedotin compared with RC and PLND alone. Table 77 and Figures 19 and 20 summarize key efficacy measures.

Table 77: Efficacy Results for Perioperative Intravenous Pembrolizumab with Enfortumab Vedotin in KEYNOTE-905
Endpoint | Intravenous Pembrolizumab 200 mg every 3 weeks in combination with enfortumab vedotin before and after RC with PLND n=170 | RC with PLND alone n=174
EFS
Number of patients with event (%) | 48 (28%) | 95 (55%)
Median in months [Based on Kaplan-Meier estimates] (95% CI) | NR (37.3, NR) | 15.7 (10.3, 20.5)
Hazard ratio [Based on stratified Cox regression model with Efron’s method of tie handling with treatment as a covariate] (95% CI) | 0.40 (0.28, 0.57)
p-Value [Based on stratified log-rank test] | <0.0001
OS
Number of patients with event (%) | 38 (22%) | 68 (39%)
Median in months (95% CI) | NR (NR, NR) | 41.7 (31.8, NR)
Hazard ratio (95% CI) | 0.50 (0.33, 0.74)
p-Value | 0.0002
NR = not reached
EFS is defined as time from randomization to the first of: disease progression preventing curative surgery, failure to undergo surgery for participants with muscle invasive residual disease, incomplete surgical resection, local or distant recurrence after surgery, or death.

Figure 19: Kaplan-Meier Curve for Event-Free Survival by Treatment Arm in KEYNOTE-905

Figure 20: Kaplan-Meier Curve for Overall Survival by Treatment Arm in KEYNOTE-905

The trial demonstrated a statistically significant difference in pCR rate (57.1% [95% CI: 49.3, 64.6] vs. 8.6% [95% CI: 4.9, 13.8]; p<0.0001).

BCG-unresponsive High-Risk Non-Muscle Invasive Bladder Cancer

The efficacy of intravenous pembrolizumab was investigated in KEYNOTE-057 (NCT02625961), a multicenter, open-label, single-arm trial in 96 patients with Bacillus Calmette-Guerin (BCG)-unresponsive, high-risk, non-muscle invasive bladder cancer (NMIBC) with carcinoma in situ (CIS) with or without papillary tumors who are ineligible for or have elected not to undergo cystectomy. BCG-unresponsive high-risk NMIBC was defined as persistent disease despite adequate BCG therapy, disease recurrence after an initial tumor-free state following adequate BCG therapy, or T1 disease following a single induction course of BCG. Adequate BCG therapy was defined as administration of at least five of six doses of an initial induction course plus either of: at least two of three doses of maintenance therapy or at least two of six doses of a second induction course. Prior to treatment, all patients had undergone transurethral resection of bladder tumor (TURBT) to remove all resectable disease (Ta and T1 components). Residual CIS (Tis components) not amenable to complete resection was allowed. The trial excluded patients with muscle invasive (i.e., T2, T3, T4) locally advanced non-resectable or metastatic urothelial carcinoma, concurrent extra-vesical (i.e., urethra, ureter or renal pelvis) non-muscle invasive transitional cell carcinoma of the urothelium, or autoimmune disease or a medical condition that required immunosuppression.

Patients received intravenous pembrolizumab 200 mg every 3 weeks until unacceptable toxicity, persistent or recurrent high-risk NMIBC, or progressive disease. Assessment of tumor status was performed every 12 weeks for two years and then every 24 weeks for three years, and patients without disease progression could be treated for up to 24 months. The major efficacy outcome measures were complete response (as defined by negative results for cystoscopy [with TURBT/biopsies as applicable], urine cytology, and computed tomography urography [CTU] imaging) and duration of response.

The study population characteristics were: median age of 73 years (range: 44 to 92); 44% age ≥75; 84% male; 67% White; and 73% and 27% with an ECOG performance status of 0 or 1, respectively. Tumor pattern at study entry was CIS with T1 (13%), CIS with high grade TA (25%), and CIS (63%). Baseline high-risk NMIBC disease status was 27% persistent and 73% recurrent. The median number of prior instillations of BCG was 12.

The median follow-up time was 28.0 months (range: 4.6 to 40.5 months). Efficacy results are summarized in Table 78.

Table 78: Efficacy Results in KEYNOTE-057
Endpoint | Intravenous Pembrolizumab 200 mg every 3 weeks n=96
Complete Response Rate (95% CI) | 41% (31, 51)
Duration of Response [Based on patients (n=39) that achieved a complete response; reflects period from the time complete response was achieved]
Median in months (range) | 16.2 (0.0+, 30.4+)
% (n) with duration ≥12 months | 46% (18)
+ Denotes ongoing response

14.7 Microsatellite Instability-High or Mismatch Repair Deficient Cancer

The efficacy of intravenous pembrolizumab was investigated in 504 patients with MSI-H or dMMR cancers enrolled in three multicenter, non-randomized, open-label, multi-cohort trials: KEYNOTE-164 (NCT02460198), KEYNOTE-158 (NCT02628067), and KEYNOTE-051 (NCT02332668). All trials excluded patients with autoimmune disease or a medical condition that required immunosuppression. Regardless of histology, MSI or MMR tumor status was determined using polymerase chain reaction (PCR; local or central) or immunohistochemistry (IHC; local or central), respectively.

- KEYNOTE-164 enrolled 124 patients with advanced MSI-H or dMMR colorectal cancer (CRC) that progressed following treatment with fluoropyrimidine and either oxaliplatin or irinotecan +/- anti-VEGF/EGFR mAb-based therapy.
- KEYNOTE-158 enrolled 373 patients with advanced MSI-H or dMMR non-colorectal cancers (non-CRC) who had disease progression following prior therapy. Patients were either prospectively enrolled with MSI-H/dMMR tumors (Cohort K) or retrospectively identified in one of 10 solid tumor cohorts (Cohorts A-J).
- KEYNOTE-051 enrolled 7 pediatric patients with MSI-H or dMMR cancers.

Adult patients received intravenous pembrolizumab 200 mg every 3 weeks (pediatric patients received 2 mg/kg every 3 weeks) until unacceptable toxicity, disease progression, or a maximum of 24 months. In KEYNOTE-164 and KEYNOTE-158, assessment of tumor status was performed every 9 weeks through the first year, then every 12 weeks thereafter. In KEYNOTE-051, assessment of tumor status was performed every 8 weeks for 24 weeks, and then every 12 weeks thereafter. The major efficacy outcome measures were ORR and DoR as assessed by BICR according to RECIST v1.1 (modified to follow a maximum of 10 target lesions and a maximum of 5 target lesions per organ in KEYNOTE-158) and as assessed by the investigator according to RECIST v1.1 in KEYNOTE-051.

In KEYNOTE-164 and KEYNOTE-158, the study population characteristics were median age of 60 years, 36% age 65 or older; 44% male; 78% White, 14% Asian, 4% American Indian or Alaska Native, and 3% Black; and 45% ECOG PS of 0 and 55% ECOG PS of 1. Ninety-two percent of patients had metastatic disease and 4% had locally advanced, unresectable disease. Thirty-seven percent of patients received one prior line of therapy and 61% received two or more prior lines of therapy.

In KEYNOTE-051, the study population characteristics were median age of 11 years (range: 3 to 16); 71% female; 86% White and 14% Asian; and 57% had a Lansky/Karnofsky Score of 100. Seventy-one percent of patients had Stage IV and 14% had Stage III disease. Fifty-seven percent of patients received one prior line of therapy and 29% received two prior lines of therapy.

Discordant results were observed between local MSI-H or dMMR tests and central testing among patients enrolled in Cohort K of KEYNOTE-158. Among 104 tumor samples that were MSI-H or dMMR by local testing and also tested using the FoundationOne®CDx (F1CDx) test, 59 (56.7%) were MSI-H and 45 (43.3%) were not MSI-H. Among 169 tumor samples that were MSI-H or dMMR by local testing and also tested using the VENTANA MMR RxDx Panel, 105 (62.1%) were dMMR and 64 (37.9%) were pMMR.

Efficacy results are summarized in Tables 79 and 80.

Table 79: Efficacy Results for Patients with MSI-H/dMMR Cancer
Endpoint | Intravenous Pembrolizumab n=504 [Median follow-up time of 20.1 months (range 0.1 to 71.4 months)]
Objective Response Rate
ORR (95% CI) [Of the 7 pediatric patients from KEYNOTE-051, 1 patient had a radiographic complete response after initial growth of their tumor but is not reflected in the results.] | 33.3% (29.2, 37.6)
Complete response rate | 10.3%
Partial response rate | 23.0%
Duration of Response | n=168
Median in months (range) | 63.2 (1.9+, 63.9+)
% with duration ≥12 months | 77%
% with duration ≥36 months | 39%
+ Denotes ongoing response

Table 80: Response by Tumor Type
 |  | Objective Response Rate |  | Duration of Response range
 | N | n (%) | 95% CI | (months)
CRC | 124 | 42 (34%) | (26%, 43%) | (4.4, 58.5+)
Non-CRC [Results include patients in Cohort K of KEYNOTE-158 that were later determined to be pMMR or not MSI-H by central testing] | 380 | 126 (33%) | (28%, 38%) | (1.9+, 63.9+)
Endometrial cancer | 94 | 47 (50%) | (40%, 61%) | (2.9, 63.2)
Gastric or GE junction cancer | 51 | 20 (39%) | (26%, 54%) | (1.9+, 63.0+)
Small intestinal cancer | 27 | 16 (59%) | (39%, 78%) | (3.7+, 57.3+)
Brain cancer | 27 [Includes 6 pediatric patients with brain cancer] | 1 (4%) [In addition to the 1 adult responder, 1 pediatric patient had a radiographic complete response after initial growth of their tumor.] | (0%, 19%) | 18.9
Ovarian cancer | 25 | 8 (32%) | (15%, 54%) | (4.2, 56.6+)
Biliary cancer | 22 | 9 (41%) | (21%, 64%) | (6.2, 49.0+)
Pancreatic cancer | 22 | 4 (18%) | (5%, 40%) | (8.1, 24.3+)
Sarcoma | 14 | 3 (21%) | (5%, 51%) | (35.4+, 57.2+)
Breast cancer | 13 | 1 (8%) | (0%,36%) | 24.3+
Other [Includes tumor type (n): anal (3), HNSCC (1), nasopharyngeal (1), retroperitoneal (1), testicular (1), vaginal (1), vulvar (1), appendiceal adenocarcinoma, NOS (1), hepatocellular carcinoma (1), and carcinoma of unknown origin (1). Includes 1 pediatric patient with abdominal adenocarcinoma.] | 13 | 4 (31%) | (9%, 61%) | (6.2+, 32.3+)
Cervical cancer | 11 | 1 (9%) | (0%, 41%) | 63.9+
Neuroendocrine cancer | 11 | 1 (9%) | (0%, 41%) | 13.3
Prostate cancer | 8 | 1 (13%) | (0%, 53%) | 24.5+
Adrenocortical cancer | 7 | 1 (14%) | (0%, 58%) | 4.2
Mesothelioma | 7 | 0 (0%) | (0%, 41%)
Thyroid cancer | 7 | 1 (14%) | (0%, 58%) | 8.2
Small cell lung cancer | 6 | 2 (33%) | (4%, 78%) | (20.0, 47.5)
Bladder cancer | 6 | 3 (50%) | (12%, 88%) | (35.6+, 57.5+)
Salivary cancer | 5 | 2 (40%) | (5%, 85%) | (42.6+, 57.8+)
Renal cell cancer | 4 | 1 (25%) | (0%, 81%) | 22.0
+ Denotes ongoing response

Exploratory analysis by TMB

In an exploratory analysis performed in 138 patients (Cohort K of KEYNOTE-158) who were tested retrospectively for tumor mutation burden (TMB) using an FDA-authorized test, 45 (33%) had tumors with TMB score of <10 mut/Mb; ORR in these 45 patients was 6.7% (95% CI: 1.4, 18.3). Among the 45 patients with TMB score of <10 mut/Mb, 39 of the patients were pMMR/not MSI-H when tested using an FDA-authorized test.

14.8 Microsatellite Instability-High or Mismatch Repair Deficient Colorectal Cancer

The efficacy of intravenous pembrolizumab was investigated in KEYNOTE-177 (NCT02563002), a multicenter, randomized, open-label, active-controlled trial that enrolled 307 patients with previously untreated unresectable or metastatic MSI-H or dMMR CRC. MSI or MMR tumor status was determined locally using polymerase chain reaction (PCR) or immunohistochemistry (IHC), respectively. Patients with autoimmune disease or a medical condition that required immunosuppression were ineligible.

Patients were randomized (1:1) to receive intravenous pembrolizumab 200 mg intravenously every 3 weeks or investigator’s choice of the following chemotherapy regimens given intravenously every 2 weeks:

- mFOLFOX6 (oxaliplatin, leucovorin, and FU) or mFOLFOX6 in combination with either bevacizumab or cetuximab: Oxaliplatin 85 mg/m^2, leucovorin 400 mg/m^2 (or levoleucovorin 200 mg/m^2), and FU 400 mg/m^2 bolus on Day 1, then FU 2400 mg/m^2 over 46-48 hours. Bevacizumab 5 mg/kg on Day 1 or cetuximab 400 mg/m^2 on first infusion, then 250 mg/m^2 weekly.
- FOLFIRI (irinotecan, leucovorin, and FU) or FOLFIRI in combination with either bevacizumab or cetuximab: Irinotecan 180 mg/m^2, leucovorin 400 mg/m^2 (or levoleucovorin 200 mg/m^2), and FU 400 mg/m^2 bolus on Day 1, then FU 2400 mg/m^2 over 46-48 hours. Bevacizumab 5 mg/kg on Day 1 or cetuximab 400 mg/m^2 on first infusion, then 250 mg/m^2 weekly.

Treatment with intravenous pembrolizumab or chemotherapy continued until RECIST v1.1-defined progression of disease as determined by the investigator or unacceptable toxicity. Patients treated with intravenous pembrolizumab without disease progression could be treated for up to 24 months. Assessment of tumor status was performed every 9 weeks. Patients randomized to chemotherapy were offered intravenous pembrolizumab at the time of disease progression. The main efficacy outcome measures were PFS (as assessed by BICR according to RECIST v1.1, modified to follow a maximum of 10 target lesions and a maximum of 5 target lesions per organ) and OS. Additional efficacy outcome measures were ORR and DoR.

A total of 307 patients were enrolled and randomized to intravenous pembrolizumab (n=153) or chemotherapy (n=154). The baseline characteristics of these 307 patients were: median age of 63 years (range: 24 to 93), 47% age 65 or older; 50% male; 75% White and 16% Asian; 52% had an ECOG PS of 0 and 48% had an ECOG PS of 1; and 27% received prior adjuvant or neoadjuvant chemotherapy. Among 154 patients randomized to receive chemotherapy,143 received chemotherapy per the protocol. Of the 143 patients, 56% received mFOLFOX6, 44% received FOLFIRI, 70% received bevacizumab plus mFOLFOX6 or FOLFIRI, and 11% received cetuximab plus mFOLFOX6 or FOLFIRI.

The trial demonstrated a statistically significant improvement in PFS for patients randomized to intravenous pembrolizumab compared with chemotherapy. There was no statistically significant difference between intravenous pembrolizumab and chemotherapy in the final OS analysis. Sixty percent of the patients who had been randomized to receive chemotherapy had crossed over to receive subsequent anti-PD-1/PD-L1 therapies including intravenous pembrolizumab. The median follow-up time at the final analysis was 38.1 months (range: 0.2 to 58.7 months). Table 81 and Figure 21 summarize the key efficacy measures for KEYNOTE-177.

Table 81: Efficacy Results in Patients with MSI-H or dMMR CRC in KEYNOTE-177
Endpoint | Intravenous Pembrolizumab 200 mg every 3 weeks n=153 | Chemotherapy n=154
PFS
Number (%) of patients with event | 82 (54%) | 113 (73%)
Median in months (95% CI) | 16.5 (5.4, 32.4) | 8.2 (6.1, 10.2)
Hazard ratio [Based on Cox regression model] (95% CI) | 0.60 (0.45, 0.80)
p-Value [Two-sided p-Value based on log-rank test (compared to a significance level of 0.0234)] | 0.0004
OS [Final OS analysis]
Number (%) of patients with event | 62 (41%) | 78 (51%)
Median in months (95% CI) | NR (49.2, NR) | 36.7 (27.6, NR)
Hazard ratio (95% CI) | 0.74 (0.53, 1.03)
p-Value [Two-sided p-Value based on log-rank test (compared to a significance level of 0.0492)] | 0.0718
Objective Response Rate [Based on confirmed response by BICR review]
ORR (95% CI) | 44% (35.8, 52.0) | 33% (25.8, 41.1)
Complete response rate | 11% | 4%
Partial response rate | 33% | 29%
Duration of Response, [Based on n=67 patients with a response in the intravenous pembrolizumab arm and n=51 patients with a response in the chemotherapy arm]
Median in months (range) | NR (2.3+, 41.4+) | 10.6 (2.8, 37.5+)
% with duration ≥12 months [Based on observed duration of response] | 75% | 37%
% with duration ≥24 months | 43% | 18%
+ Denotes ongoing response
NR = not reached

Figure 21: Kaplan-Meier Curve for PFS in KEYNOTE-177

14.9 Gastric Cancer

First-line Treatment of Locally Advanced Unresectable or Metastatic HER2-Positive Gastric or Gastroesophageal Junction Adenocarcinoma for Tumors Expressing PD-L1 (CPS ≥1)

The efficacy of intravenous pembrolizumab in combination with trastuzumab plus fluoropyrimidine and platinum chemotherapy was investigated in KEYNOTE-811 (NCT03615326), a multicenter, randomized, double-blind, placebo-controlled trial that enrolled 698 patients with HER2-positive advanced gastric or gastroesophageal junction (GEJ) adenocarcinoma who had not previously received systemic therapy for metastatic disease. PD-L1 status was determined using the PD-L1 IHC 22C3 pharmDx assay. Patients with an autoimmune disease that required systemic therapy within 2 years of treatment or a medical condition that required immunosuppression were ineligible. Randomization was stratified by PD-L1 expression (CPS ≥1 or CPS <1), chemotherapy regimen (5-FU plus cisplatin [FP] or capecitabine plus oxaliplatin [CAPOX]), and geographic region (Europe/Israel/North America/Australia, Asia, or Rest of the World). Patients were randomized (1:1) to one of the following treatment arms:

- Intravenous pembrolizumab 200 mg, trastuzumab 8 mg/kg on first infusion and 6 mg/kg in subsequent cycles, followed by investigator’s choice of combination chemotherapy of cisplatin 80 mg/m^2 for up to 6 cycles and 5-FU 800 mg/m^2/day for 5 days (FP) or oxaliplatin 130 mg/m^2 up to 6-8 cycles and capecitabine 1000 mg/m^2 bid for 14 days (CAPOX).
- Placebo, trastuzumab 8 mg/kg on first infusion and 6 mg/kg in subsequent cycles, followed by investigator’s choice of combination chemotherapy of cisplatin 80 mg/m^2 for up to 6 cycles and 5-FU 800 mg/m^2/day for 5 days (FP) or oxaliplatin 130 mg/m^2 up to 6-8 cycles and capecitabine 1000 mg/m^2 bid for 14 days (CAPOX).

All study medications, except oral capecitabine, were administered as an intravenous infusion every 3-week cycle. Treatment with intravenous pembrolizumab continued until RECIST v1.1-defined progression of disease as determined by BICR, unacceptable toxicity, or a maximum of 24 months. The major outcome measures assessed were PFS by BICR using RECIST v1.1, modified to follow a maximum of 10 target lesions and a maximum of 5 target lesions per organ, and OS.

Additional outcome measures included ORR and DoR, based on BICR using RECIST 1.1, modified to follow a maximum of 10 target lesions and a maximum of 5 target lesions per organ.

Among the 698 patients randomized, 594 (85%) had tumors that expressed PD-L1 with a CPS ≥1. PD-L1 status was determined using the PD-L1 IHC 22C3 pharmDx assay. The population characteristics of these 594 patients were: median age of 63 years (range: 19 to 85), 43% age 65 or older; 80% male; 63% White, 33% Asian, and 0.7% Black; 42% ECOG PS of 0 and 58% ECOG PS of 1. Ninety-eight percent of patients had metastatic disease (Stage IV) and 2% had locally advanced unresectable disease. Ninety-five percent (n=562) had tumors that were not MSI-H, 1% (n=8) had tumors that were MSI-H, and in 4% (n=24) the status was not known. Eighty-five percent of patients received CAPOX.

A statistically significant improvement in OS and PFS was demonstrated in patients randomized to intravenous pembrolizumab in combination with trastuzumab and chemotherapy compared with placebo in combination with trastuzumab and chemotherapy; however, an exploratory analysis of OS in the PD-L1 CPS <1 population showed a HR of 1.10 (95% CI: 0.72, 1.68), indicating that the improvement in the ITT population was primarily attributed to the results observed in the subgroup of patients with PD-L1 CPS ≥1.

Efficacy results at the final analysis for the subgroup of patients whose tumors expressed PD-L1 with a CPS ≥1 are summarized in Table 82 and Figure 22.

Table 82: Efficacy Results for KEYNOTE-811 with PD-L1 Expression CPS ≥1
Endpoint | Intravenous Pembrolizumab 200 mg every 3 weeks Trastuzumab Fluoropyrimidine and Platinum Chemotherapy n=298 | Placebo Trastuzumab Fluoropyrimidine and Platinum Chemotherapy n=296
OS
Number (%) of patients with event | 226 (76%) | 244 (82%)
Median in months [Based on Kaplan-Meier estimation] (95% CI) | 20.1 (17.9, 22.9) | 15.7 (13.5, 18.5)
Hazard ratio [Based on the unstratified Cox proportional hazard model] (95% CI) | 0.79 (0.66, 0.95)
PFS
Number (%) of patients with event | 221 (74%) | 226 (76%)
Median in months (95% CI) | 10.9 (8.5, 12.5) | 7.3 (6.8, 8.4)
Hazard ratio (95% CI) | 0.72 (0.60, 0.87)
Objective Response Rate
ORR [Response: Best objective response as confirmed complete response or partial response] (95% CI) | 73% (68, 78) | 58% (53, 64)
Complete response rate | 17% | 10%
Partial response rate | 56% | 48%
Duration of Response | n=218 | n=173
Median in months (95% CI) Range in months | 11.3 (9.9, 13.7) 1.1+, 60.8+ | 9.6 (7.1, 11.2) 1.4+, 60.5+
+ Denotes ongoing response

Figure 22: Kaplan-Meier Curve for Overall Survival by Treatment Arm in KEYNOTE-811 (CPS ≥1)

First-line Treatment of Locally Unresectable or Metastatic HER2-Negative Gastric or Gastroesophageal Junction Adenocarcinoma for Tumors Expressing PD-L1 (CPS ≥1)

The efficacy of intravenous pembrolizumab in combination with fluoropyrimidine- and platinum-containing chemotherapy was investigated in KEYNOTE-859 (NCT03675737), a multicenter, randomized, double-blind, placebo-controlled trial that enrolled 1579 patients with HER2-negative advanced gastric or GEJ adenocarcinoma who had not previously received systemic therapy for metastatic disease. Patients with an autoimmune disease that required systemic therapy within 2 years of treatment or a medical condition that required immunosuppression were ineligible. Randomization was stratified by PD-L1 expression (CPS ≥1 or CPS <1), chemotherapy regimen (FP or CAPOX), and geographic region (Europe/Israel/North America/Australia, Asia, or Rest of the World). Patients were randomized (1:1) to one of the following treatment arms:

- Intravenous pembrolizumab 200 mg, investigator’s choice of combination chemotherapy of cisplatin 80 mg/m^2 and 5-FU 800 mg/m^2/day for 5 days (FP) or oxaliplatin 130 mg/m^2 and capecitabine 1000 mg/m^2 bid for 14 days (CAPOX).
- Placebo, investigator’s choice of combination chemotherapy of cisplatin 80 mg/m^2 and 5-FU 800 mg/m^2/day for 5 days (FP) or oxaliplatin 130 mg/m^2 and capecitabine 1000 mg/m^2 bid for 14 days (CAPOX).

All study medications, except oral capecitabine, were administered as an intravenous infusion every 3-week cycle. Platinum agents could be administered for 6 or more cycles following local guidelines. Treatment with intravenous pembrolizumab continued until RECIST v1.1-defined progression of disease as determined by BICR, unacceptable toxicity, or a maximum of 24 months. The major efficacy outcome measure was OS. Additional secondary efficacy outcome measures included PFS, ORR, and DoR as assessed by BICR using RECIST v1.1, modified to follow a maximum of 10 target lesions and a maximum of 5 target lesions per organ.

Among 1,579 patients, 1,235 (78%) had tumors expressing PD-L1 CPS ≥ 1. The population characteristics in patients with PD-L1 CPS ≥ 1 expressing tumors were: median age of 62 years (range: 24 to 86), 40% age 65 or older; 70% male and 30% female; 55% White, 33% Asian, 4.6% Multiple, 4.3% American Indian or Alaskan Native, 1.3% Black, and 0.2% Native Hawaiian or other Pacific Islander; 76% Not Hispanic or Latino and 21% Hispanic or Latino; 37% ECOG PS of 0 and 63% ECOG PS of 1. Ninety-six percent of patients had metastatic disease (Stage IV) and 3% had locally advanced unresectable disease. Five percent (n=66) had tumors that were MSI-H. Eighty-six percent of patients received CAPOX.

A statistically significant improvement in OS, PFS, and ORR was demonstrated in patients randomized to intravenous pembrolizumab in combination with chemotherapy compared with placebo in combination with chemotherapy at the time of a pre-specified interim analysis of OS; however, an exploratory analysis of OS in the PD-L1 CPS <1 population showed a HR of 0.92 (95% CI 0.73, 1.17) indicating that the improvement in the ITT population was primarily attributed to the results observed in the subgroup of patients with PD-L1 CPS ≥1. Efficacy results for patients whose tumors expressed PD-L1 CPS ≥1 and CPS ≥10 are summarized in Table 83 and Figures 23 and 24.

Table 83: Efficacy Results [Based on a pre-specified interim analysis] for KEYNOTE-859
Endpoint | Intravenous Pembrolizumab 200 mg every 3 weeks and FP or CAPOX n=618 | Placebo and FP or CAPOX n=617 | Intravenous Pembrolizumab 200 mg every 3 weeks and FP or CAPOX n=279 | Placebo and FP or CAPOX n=272
 | CPS ≥1 |  | CPS ≥10
OS
Number (%) of patients with event | 464 (75) | 526 (85) | 188 (67) | 226 (83)
Median in months (95% CI) | 13.0 (11.6, 14.2) | 11.4 (10.5, 12.0) | 15.7 (13.8, 19.3) | 11.8 (10.3, 12.7)
Hazard ratio [Based on the stratified Cox proportional hazard model] (95% CI) | 0.74 (0.65, 0.84) |  | 0.65 (0.53, 0.79)
p-Value (stratified log-rank) [One-sided p-Value based on stratified log-rank test] | <0.0001 |  | <0.0001
PFS
Number (%) of patients with event | 443 (72%) | 483 (78%) | 190 (68) | 210 (77)
Median in months (95% CI) | 6.9 (6.0, 7.2) | 5.6 (5.4, 5.7) | 8.1 (6.8, 8.5) | 5.6 (5.4, 6.7)
Hazard ratio (95% CI) | 0.72 (0.63, 0.82) |  | 0.62 (0.51, 0.76)
p-Value (stratified log-rank) | <0.0001 |  | <0.0001
Objective Response Rate
ORR [Response: Best objective response as confirmed complete response or partial response] (95% CI) | 52% (48, 56) | 43% (39, 47) | 61% (55, 66) | 43% (37, 49)
Complete response rate | 10% | 6% | 13% | 5%
Partial response rate | 42% | 37% | 48% | 38%
p-Value [One-sided p-Value based on stratified Miettinen & Nurminen method] | 0.0004 |  | <0.0001
Duration of Response | n=322 | n=263 | n=169 | n=117
Median in months [Based on Kaplan-Meier estimates] (95% CI) | 8.3 (7.0, 10.9) | 5.6 (5.4, 6.9) | 10.9 (8.0, 13.8) | 5.8 (5.3, 7.0)
Range in months | 1.2+, 41.5+ | 1.3+, 34.2+ | 1.2+, 41.5+ | 1.4+, 31.2+
+ Denotes ongoing response

Figure 23: Kaplan-Meier Curve for Overall Survival in KEYNOTE-859 (CPS ≥1)

Figure 24: Kaplan-Meier Curve for Overall Survival in KEYNOTE-859 (CPS ≥10)

An exploratory analysis of OS in the 74 patients with MSI-H tumors irrespective of PD-L1 status showed a HR of 0.34 (95% CI: 0.18, 0.66).

14.10 Esophageal Cancer

First-line Treatment of Locally Advanced Unresectable or Metastatic Esophageal/Gastroesophageal Junction Cancer for Tumors Expressing PD-L1 (CPS ≥1)

KEYNOTE-590

The efficacy of intravenous pembrolizumab was investigated in KEYNOTE-590 (NCT03189719), a multicenter, randomized, placebo-controlled trial that enrolled 749 patients with metastatic or locally advanced esophageal or gastroesophageal junction (tumors with epicenter 1 to 5 centimeters above the GEJ) carcinoma who were not candidates for surgical resection or definitive chemoradiation. PD-L1 status was centrally determined in tumor specimens in all patients using the PD-L1 IHC 22C3 pharmDx assay. Patients with active autoimmune disease, a medical condition that required immunosuppression, or who received prior systemic therapy in the locally advanced or metastatic setting were ineligible. Randomization was stratified by tumor histology (squamous cell carcinoma vs. adenocarcinoma), geographic region (Asia vs. ex-Asia), and ECOG performance status (0 vs. 1).

Patients were randomized (1:1) to one of the following treatment arms; all study medications were administered via intravenous infusion:

- Intravenous pembrolizumab 200 mg on Day 1 of each three-week cycle in combination with cisplatin 80 mg/m^2 IV on Day 1 of each three-week cycle for up to six cycles and FU 800 mg/m^2 IV per day on Day 1 to Day 5 of each three-week cycle, or per local standard for FU administration, for up to 24 months.
- Placebo on Day 1 of each three-week cycle in combination with cisplatin 80 mg/m^2 IV on Day 1 of each three-week cycle for up to six cycles and FU 800 mg/m^2 IV per day on Day 1 to Day 5 of each three-week cycle, or per local standard for FU administration, for up to 24 months.

Treatment with intravenous pembrolizumab or chemotherapy continued until unacceptable toxicity or disease progression. Patients could be treated with intravenous pembrolizumab for up to 24 months in the absence of disease progression. The major efficacy outcome measures were OS and PFS as assessed by the investigator according to RECIST v1.1 (modified to follow a maximum of 10 target lesions and a maximum of 5 target lesions per organ). The study pre-specified analyses of OS and PFS based on squamous cell histology, CPS ≥10, and in all patients. Additional efficacy outcome measures were ORR and DoR, according to modified RECIST v1.1, as assessed by the investigator. Additional analyses of efficacy outcome measures were also conducted based on PD-L1 CPS ≥1.

Among 749 patients, 647 (86%) had tumors expressing PD-L1 CPS ≥ 1. The study population characteristics in patients with PD-L1 CPS ≥ 1 expressing tumors were: median age of 63 years (range: 27 to 89), 41% age 65 or older; 83% male; 36% White, 54% Asian, and 1% Black; 40% had an ECOG PS of 0 and 59% had an ECOG PS of 1. Ninety-one percent had M1 disease and 9% had M0 disease. Seventy-four percent had a tumor histology of squamous cell carcinoma, and 26% had adenocarcinoma.

The trial demonstrated a statistically significant improvement in OS and PFS for patients randomized to intravenous pembrolizumab in combination with chemotherapy compared to chemotherapy; however, an exploratory analysis of OS in the PD-L1 CPS <1 population showed an HR of 0.96 (0.59, 1.55), indicating that the improvement in the ITT population was primarily attributed to the results observed in the subgroup of patients with PD-L1 CPS ≥1.

Table 84 and Figures 25 and 26 summarize the efficacy results for KEYNOTE-590 in patients whose tumors expressed PD-L1 CPS ≥1 and CPS ≥10.

Table 84: Efficacy Results in Patients with Locally Advanced Unresectable or Metastatic Esophageal Cancer in KEYNOTE-590
Endpoint | Intravenous Pembrolizumab 200 mg every 3 weeks Cisplatin FU n=320 | Placebo Cisplatin FU n=327 | Intravenous Pembrolizumab 200 mg every 3 weeks Cisplatin FU n=186 | Placebo Cisplatin FU n=197
 | CPS ≥1 |  | CPS ≥10
OS
Number (%) of events | 222 (69) | 271 (83) | 124 (67) | 165 (84)
Median in months (95% CI) | 12.7 (10.5, 14.4) | 9.8 (8.8, 10.8) | 13.5 (11.1, 15.6) | 9.4 (8.0, 10.7)
Hazard ratio [Based on the stratified Cox proportional hazard model] (95% CI) | 0.71 (0.59, 0.84) |  | 0.62 (0.49, 0.78)
p-Value [Based on a stratified log-rank test; p-Value for CPS ≥1 not included (not pre-specified subgroup)] |  |  | <0.0001
PFS
Number of events (%) | 252 (79) | 291 (89) | 140 (75) | 174 (88)
Median in months (95% CI) | 6.3 (6.2, 7.1) | 5.7 (4.6, 6.0) | 7.5 (6.2, 8.2) | 5.5 (4.3, 6.0)
Hazard ratio (95% CI) | 0.62 (0.52, 0.73) |  | 0.51 (0.41, 0.65)
p-Value |  |  | <0.0001
Objective Response Rate
ORR, % [Confirmed complete response or partial response] (95% CI) | 45 (40, 51) | 29 (24, 34) | 51 (44, 59) | 27 (21, 34)
Number (%) of complete responses | 19 (6) | 9 (2.8) | 11 (6) | 5 (2.5)
Number (%) of partial responses | 126 (39) | 85 (26) | 84 (45) | 48 (24)
Duration of Response
Median in months (range) | 8.6 (1.2+, 31.0+) | 5.8 (1.5+, 25.0+) | 10.4 (1.9+, 28.9+) | 5.6 (1.5+, 25.0+)

Figure 25: Kaplan-Meier Curve for Overall Survival in KEYNOTE-590 (CPS ≥1)

Figure 26: Kaplan-Meier Curve for Overall Survival in KEYNOTE-590 (CPS ≥10)

In a pre-specified formal test of OS in patients with PD-L1 CPS ≥10 (n=383), the median was 13.5 months (95% CI: 11.1, 15.6) for the intravenous pembrolizumab arm and 9.4 months (95% CI: 8.0, 10.7) for the placebo arm, with a HR of 0.62 (95% CI: 0.49, 0.78; p-Value < 0.0001). In an exploratory analysis, in patients with PD-L1 CPS <10 (n=347), the median OS was 10.5 months (95% CI: 9.7, 13.5) for the intravenous pembrolizumab arm and 10.6 months (95% CI: 8.8, 12.0) for the placebo arm, with a HR of 0.86 (95% CI: 0.68, 1.10).

Previously Treated Recurrent Locally Advanced or Metastatic Esophageal Cancer for Tumors Expressing PD-L1 (CPS≥ 10)

KEYNOTE-181

The efficacy of intravenous pembrolizumab was investigated in KEYNOTE-181 (NCT02564263), a multicenter, randomized, open-label, active-controlled trial that enrolled 628 patients with recurrent locally advanced or metastatic esophageal cancer who progressed on or after one prior line of systemic treatment for advanced disease. Patients with HER2/neu positive esophageal cancer were required to have received treatment with approved HER2/neu targeted therapy. All patients were required to have tumor specimens for PD-L1 testing at a central laboratory; PD-L1 status was determined using the PD-L1 IHC 22C3 pharmDx assay. Patients with a history of non-infectious pneumonitis that required steroids or current pneumonitis, active autoimmune disease, or a medical condition that required immunosuppression were ineligible.

Patients were randomized (1:1) to receive either intravenous pembrolizumab 200 mg every 3 weeks or investigator's choice of any of the following chemotherapy regimens, all given intravenously: paclitaxel 80-100 mg/m^2 on Days 1, 8, and 15 of every 4-week cycle, docetaxel 75 mg/m^2 every 3 weeks, or irinotecan 180 mg/m^2 every 2 weeks. Randomization was stratified by tumor histology (esophageal squamous cell carcinoma [ESCC] vs. esophageal adenocarcinoma [EAC]/Siewert type I EAC of the gastroesophageal junction [GEJ]), and geographic region (Asia vs. ex-Asia). Treatment with intravenous pembrolizumab or chemotherapy continued until unacceptable toxicity or disease progression. Patients randomized to intravenous pembrolizumab were permitted to continue beyond the first RECIST v1.1 (modified to follow a maximum of 10 target lesions and a maximum of 5 target lesions per organ)-defined disease progression if clinically stable until the first radiographic evidence of disease progression was confirmed at least 4 weeks later with repeat imaging. Patients treated with intravenous pembrolizumab without disease progression could be treated for up to 24 months. Assessment of tumor status was performed every 9 weeks. The major efficacy outcome measure was OS evaluated in the following co-primary populations: patients with ESCC, patients with tumors expressing PD-L1 CPS ≥10, and all randomized patients. Additional efficacy outcome measures were PFS, ORR, and DoR, according to RECIST v1.1, modified to follow a maximum of 10 target lesions and a maximum of 5 target lesions per organ, as assessed by BICR.

A total of 628 patients were enrolled and randomized to intravenous pembrolizumab (n=314) or investigator's treatment of choice (n=314). Of these 628 patients, 167 (27%) had ESCC that expressed PD-L1 with a CPS ≥10. Of these 167 patients, 85 patients were randomized to intravenous pembrolizumab and 82 patients to investigator's treatment of choice [paclitaxel (n=50), docetaxel (n=19), or irinotecan (n=13)]. The baseline characteristics of these 167 patients were: median age of 65 years (range: 33 to 80), 51% age 65 or older; 84% male; 32% White and 68% Asian; 38% had an ECOG PS of 0 and 62% had an ECOG PS of 1. Ninety percent had M1 disease and 10% had M0 disease. Prior to enrollment, 99% of patients had received platinum-based treatment and 84% had also received treatment with a fluoropyrimidine. Thirty-three percent of patients received prior treatment with a taxane.

The observed OS hazard ratio was 0.77 (95% CI: 0.63, 0.96) in patients with ESCC, 0.70 (95% CI: 0.52, 0.94) in patients with tumors expressing PD-L1 CPS ≥10, and 0.89 (95% CI: 0.75, 1.05) in all randomized patients. On further examination in patients whose ESCC tumors expressed PD-L1 (CPS ≥10), an improvement in OS was observed among patients randomized to intravenous pembrolizumab as compared with chemotherapy. Table 85 and Figure 27 summarize the key efficacy measures for KEYNOTE-181 for patients with ESCC CPS ≥10.

Table 85: Efficacy Results in Patients with Recurrent or Metastatic ESCC (CPS ≥10) in KEYNOTE-181
Endpoint | Intravenous Pembrolizumab 200 mg every 3 weeks n=85 | Chemotherapy n=82
OS
Number (%) of patients with event | 68 (80%) | 72 (88%)
Median in months (95% CI) | 10.3 (7.0, 13.5) | 6.7 (4.8, 8.6)
Hazard ratio [Based on the Cox regression model stratified by geographic region (Asia vs. ex-Asia)] (95% CI) | 0.64 (0.46, 0.90)
PFS
Number (%) of patients with event | 76 (89%) | 76 (93%)
Median in months (95% CI) | 3.2 (2.1, 4.4) | 2.3 (2.1, 3.4)
Hazard ratio (95% CI) | 0.66 (0.48, 0.92)
Objective Response Rate
ORR (95% CI) | 22 (14, 33) | 7 (3, 15)
Number (%) of complete responses | 4 (5) | 1 (1)
Number (%) of partial responses | 15 (18) | 5 (6)
Median duration of response in months (range) | 9.3 (2.1+, 18.8+) | 7.7 (4.3, 16.8+)

Figure 27: Kaplan-Meier Curve for Overall Survival in KEYNOTE-181 (ESCC CPS ≥10)

KEYNOTE-180

The efficacy of intravenous pembrolizumab was investigated in KEYNOTE-180 (NCT02559687), a multicenter, non-randomized, open-label trial that enrolled 121 patients with locally advanced or metastatic esophageal cancer who progressed on or after at least 2 prior systemic treatments for advanced disease. With the exception of the number of prior lines of treatment, the eligibility criteria were similar to and the dosage regimen identical to KEYNOTE-181.

The major efficacy outcome measures were ORR and DoR according to RECIST v1.1, modified to follow a maximum of 10 target lesions and a maximum of 5 target lesions per organ, as assessed by BICR.

Among the 121 patients enrolled, 29% (n=35) had ESCC that expressed PD-L1 CPS ≥10. The baseline characteristics of these 35 patients were: median age of 65 years (range: 47 to 81), 51% age 65 or older; 71% male; 26% White and 69% Asian; 40% had an ECOG PS of 0 and 60% had an ECOG PS of 1. One hundred percent had M1 disease.

The ORR in the 35 patients with ESCC expressing PD-L1 was 20% (95% CI: 8, 37). Among the 7 responding patients, the DoR ranged from 4.2 to 25.1+ months, with 5 patients (71%) having responses of 6 months or longer and 3 patients (57%) having responses of 12 months or longer.

14.11 Cervical Cancer

FIGO 2014 Stage III-IVA Cervical Cancer with Chemoradiotherapy

The efficacy of intravenous pembrolizumab in combination with CRT (cisplatin and external beam radiation therapy [EBRT] followed by brachytherapy [BT]) was investigated in KEYNOTE-A18 (NCT04221945), a multicenter, randomized, double-blind, placebo-controlled trial that enrolled 1060 patients with cervical cancer who had not previously received any definitive surgery, radiation, or systemic therapy for cervical cancer. There were 599 patients with FIGO 2014 Stage III-IVA disease (tumor involves the lower third of the vagina or the pelvic sidewall, or there is hydronephrosis/non-functioning kidney or spread to adjacent pelvic organs, all without spread to distant organs), and 459 patients with FIGO 2014 Stage IB2-IIB disease (clinical lesion >4 cm confined to the cervix, or clinical lesion of any size with extension beyond the uterus, but which has not extended to the pelvic wall or lower third of the vagina) with positive nodes. Two patients had FIGO 2014 Stage IVB disease. Randomization was stratified by planned type of EBRT (Intensity-modulated radiation therapy [IMRT] or volumetric modulated arc therapy [VMAT] vs. non-IMRT and non-VMAT), stage at screening of cervical cancer (FIGO 2014 Stage IB2-IIB vs. FIGO 2014 Stage III-IVA), and planned total radiotherapy dose (EBRT + brachytherapy dose of <70 Gy vs. ≥70 Gy as per equivalent dose [EQD2]).

Patients were randomized (1:1) to one of two treatment arms:

- Intravenous pembrolizumab 200 mg IV every 3 weeks (5 cycles) concurrent with cisplatin 40 mg/m^2 IV weekly (5 cycles, an optional sixth infusion could be administered per local practice), and radiotherapy (EBRT followed by BT), followed by intravenous pembrolizumab 400 mg IV every 6 weeks (15 cycles)
- Placebo IV every 3 weeks (5 cycles) concurrent with cisplatin 40 mg/m^2 IV weekly (5 cycles, an optional sixth infusion could be administered per local practice), and radiotherapy (EBRT followed by BT), followed by placebo IV every 6 weeks (15 cycles)

Treatment continued until RECIST v1.1-defined progression of disease as determined by investigator or unacceptable toxicity.

Assessment of tumor status was performed every 12 weeks from completion of CRT for the first two years, followed by every 24 weeks in year 3, and then annually. The major efficacy outcome measures were PFS as assessed by investigator according to RECIST v1.1, modified to follow a maximum of 10 target lesions and a maximum of 5 target lesions per organ, or histopathologic confirmation, and OS.

Among the 599 patients with FIGO 2014 Stage III-IVA disease, the baseline characteristics were: median age of 52 years (range: 22 to 87), 17% age 65 or older; 36% White, 34% Asian, 2% Black; 38% Hispanic or Latino; 68% ECOG PS 0 and 32% ECOG PS 1; 93% with CPS ≥1; 71% had positive pelvic and/or positive para-aortic lymph node(s) and 29% had neither positive pelvic nor para-aortic lymph node(s); 83% had squamous cell carcinoma and 17% had non-squamous histology. Regarding radiation, 86% of patients received IMRT or VMAT EBRT, and the median EQD2 dose was 87 Gy (range: 7 to 114).

The trial demonstrated statistically significant improvements in PFS and OS in the ITT population. Exploratory analyses of PFS and OS by the stratification factor of FIGO 2014 stage showed that the improvement in the ITT population was primarily attributed to the results seen in the patients with FIGO 2014 Stage III-IVA disease. Table 86 and Figures 28 and 29 summarize the results in exploratory subgroup analyses of 599 patients with FIGO 2014 Stage III-IVA disease.

Table 86: Efficacy Results in KEYNOTE-A18 (Patients with FIGO 2014 Stage III-IVA Cervical Cancer)
Endpoint | Intravenous Pembrolizumab 200 mg every 3 weeks and 400 mg every 6 weeks with CRT n=295 | Placebo with CRT n=304
OS [Results at the time of pre-specified final analysis for OS]
Number of patients with event (%) | 61 (21) | 90 (30)
Hazard ratio [Based on the unstratified Cox proportional hazard model] (95% CI) | 0.65 (0.47, 0.90)
PFS by Investigator [Results at the time of first pre-specified interim analysis for PFS]
Number of patients with event (%) | 61 (21) | 94 (31)
Median in months (95% CI) | NR (NR, NR) | NR (18.8, NR)
12-month PFS rate (95% CI) | 81% (75, 85) | 70% (64, 76)
Hazard ratio (95% CI) | 0.59 (0.43, 0.81)
CRT = Chemoradiotherapy
NR = not reached

Figure 28: Kaplan-Meier Curve for Overall Survival in KEYNOTE-A18 (Patients with FIGO 2014 Stage III-IVA Cervical Cancer)

Figure 29: Kaplan-Meier Curve for Progression-Free Survival in KEYNOTE-A18 (Patients with FIGO 2014 Stage III-IVA Cervical Cancer)

Persistent, Recurrent, or Metastatic Cervical Cancer for Tumors Expressing PD-L1 (CPS ≥1)

The efficacy of intravenous pembrolizumab in combination with paclitaxel and cisplatin or paclitaxel and carboplatin, with or without bevacizumab, was investigated in KEYNOTE-826 (NCT03635567), a multicenter, randomized, double-blind, placebo-controlled trial that enrolled 617 patients with persistent, recurrent, or first-line metastatic cervical cancer who had not been treated with chemotherapy except when used concurrently as a radio-sensitizing agent. Patients were enrolled regardless of tumor PD-L1 expression status. Patients with autoimmune disease that required systemic therapy within 2 years of treatment or a medical condition that required immunosuppression were ineligible. Randomization was stratified by metastatic status at initial diagnosis, investigator decision to use bevacizumab, and PD-L1 status (CPS <1 vs. CPS 1 to <10 vs. CPS ≥10). Patients were randomized (1:1) to one of the two treatment groups:

- Treatment Group 1: Intravenous pembrolizumab 200 mg plus chemotherapy with or without bevacizumab
- Treatment Group 2: Placebo plus chemotherapy with or without bevacizumab

The investigator selected one of the following four treatment regimens prior to randomization:

1. Paclitaxel 175 mg/m^2 + cisplatin 50 mg/m^2
2. Paclitaxel 175 mg/m^2 + cisplatin 50 mg/m^2 + bevacizumab 15 mg/kg
3. Paclitaxel 175 mg/m^2 + carboplatin AUC 5 mg/mL/min
4. Paclitaxel 175 mg/m^2 + carboplatin AUC 5 mg/mL/min + bevacizumab 15 mg/kg

All study medications were administered as an intravenous infusion. All study treatments were administered on Day 1 of each 3-week treatment cycle. Cisplatin could be administered on Day 2 of each 3-week treatment cycle. Treatment with intravenous pembrolizumab continued until RECIST v1.1-defined progression of disease, unacceptable toxicity, or a maximum of 24 months. Administration of intravenous pembrolizumab was permitted beyond RECIST-defined disease progression if the patient was clinically stable and considered to be deriving clinical benefit by the investigator. Assessment of tumor status was performed every 9 weeks for the first year, followed by every 12 weeks thereafter. The main efficacy outcome measures were OS and PFS as assessed by investigator according to RECIST v1.1, modified to follow a maximum of 10 target lesions and a maximum of 5 target lesions per organ. Additional efficacy outcome measures were ORR and DoR, according to RECIST v1.1, as assessed by investigator.

Of the 617 enrolled patients, 548 patients (89%) had tumors expressing PD-L1 with a CPS ≥1. Among these 548 enrolled patients with tumors expressing PD-L1, 273 patients were randomized to intravenous pembrolizumab in combination with chemotherapy with or without bevacizumab, and 275 patients were randomized to placebo in combination with chemotherapy with or without bevacizumab. Sixty-three percent of the 548 patients received bevacizumab as part of study treatment. The baseline characteristics of the 548 patients were: median age of 51 years (range: 22 to 82), 16% age 65 or older; 59% White, 18% Asian, 6% American Indian or Alaska Native, and 1% Black; 37% Hispanic or Latino; 56% ECOG performance status 0 and 43% ECOG performance status 1. Seventy-five percent had squamous cell carcinoma, 21% adenocarcinoma, and 5% adenosquamous histology, and 32% of patients had metastatic disease at diagnosis. At study entry, 21% of patients had metastatic disease only and 79% had persistent or recurrent disease with or without distant metastases, of whom 39% had received prior chemoradiation only and 17% had received prior chemoradiation plus surgery.

A statistically significant improvement in OS and PFS was demonstrated in patients randomized to receive intravenous pembrolizumab compared with patients randomized to receive placebo. An updated OS analysis was conducted at the time of final analysis when 354 deaths in the CPS ≥1 population were observed. Table 87 and Figure 30 summarize the key efficacy measures for KEYNOTE-826 for patients with tumors expressing PD-L1 (CPS ≥1).

Table 87: Efficacy Results in Patients with Persistent, Recurrent, or Metastatic Cervical Cancer (CPS ≥1) in KEYNOTE-826
Endpoint | Intravenous Pembrolizumab 200 mg every 3 weeks and chemotherapy [Chemotherapy (paclitaxel and cisplatin or paclitaxel and carboplatin)] with or without bevacizumab n=273 | Placebo and chemotherapy with or without bevacizumab n=275
OS
Number of patients with event (%) | 118 (43.2) | 154 (56.0)
Median in months (95% CI) | NR (19.8, NR) | 16.3 (14.5, 19.4)
Hazard ratio [Based on the stratified Cox proportional hazard model] (95% CI) | 0.64 (0.50, 0.81)
p-Value [p-Value (one-sided) is compared with the allocated alpha of 0.0055 for this interim analysis (with 72% of the planned number of events for final analysis)] | 0.0001
Updated OS
Number of patients with event (%) | 153 (56.0%) | 201 (73.1%)
Median in months (95% CI) | 28.6 (22.1, 38.0) | 16.5 (14.5, 20.0)
Hazard ratio (95% CI) | 0.60 (0.49, 0.74)
PFS
Number of patients with event (%) | 157 (57.5) | 198 (72.0)
Median in months (95% CI) | 10.4 (9.7, 12.3) | 8.2 (6.3, 8.5)
Hazard ratio (95% CI) | 0.62 (0.50, 0.77)
p-Value [p-Value (one-sided) is compared with the allocated alpha of 0.0014 for this interim analysis (with 82% of the planned number of events for final analysis)] | < 0.0001
Objective Response Rate
ORR [Response: Best objective response as confirmed complete response or partial response] (95% CI) | 68% (62, 74) | 50% (44, 56)
Complete response rate | 23% | 13%
Partial response rate | 45% | 37%
Duration of Response
Median in months (range) | 18.0 (1.3+, 24.2+) | 10.4 (1.5+, 22.0+)
+ Denotes ongoing response
NR = not reached

Figure 30: Kaplan-Meier Curve for Overall Survival in KEYNOTE-826 (CPS ≥1) [Treatment arms include intravenous pembrolizumab plus chemotherapy, with or without bevacizumab, versus placebo plus chemotherapy, with or without bevacizumab.] , [Based on the protocol-specified final OS analysis]

Previously Treated Recurrent or Metastatic Cervical Cancer for Tumors Expressing PD-L1 (CPS≥ 1)

The efficacy of intravenous pembrolizumab was investigated in 98 patients with recurrent or metastatic cervical cancer enrolled in a single cohort (Cohort E) in KEYNOTE-158 (NCT02628067), a multicenter, non-randomized, open-label, multi-cohort trial. The trial excluded patients with autoimmune disease or a medical condition that required immunosuppression. Patients received intravenous pembrolizumab 200 mg intravenously every 3 weeks until unacceptable toxicity or documented disease progression. Patients with initial radiographic disease progression could receive additional doses of treatment during confirmation of progression unless disease progression was symptomatic, was rapidly progressive, required urgent intervention, or occurred with a decline in performance status. Patients without disease progression could be treated for up to 24 months. Assessment of tumor status was performed every 9 weeks for the first 12 months, and every 12 weeks thereafter. The major efficacy outcome measures were ORR according to RECIST v1.1, modified to follow a maximum of 10 target lesions and a maximum of 5 target lesions per organ, as assessed by BICR, and DoR.

Among the 98 patients in Cohort E, 77 (79%) had tumors that expressed PD-L1 with a CPS ≥ 1 and received at least one line of chemotherapy in the metastatic setting. PD-L1 status was determined using the IHC 22C3 pharmDx assay. The baseline characteristics of these 77 patients were: median age of 45 years (range: 27 to 75); 81% White, 14% Asian, and 3% Black; 32% ECOG PS of 0 and 68% ECOG PS of 1; 92% had squamous cell carcinoma, 6% adenocarcinoma, and 1% adenosquamous histology; 95% had M1 disease and 5% had recurrent disease; and 35% had one and 65% had two or more prior lines of therapy in the recurrent or metastatic setting.

No responses were observed in patients whose tumors did not have PD-L1 expression (CPS <1). Efficacy results are summarized in Table 88 for patients with PD-L1 expression (CPS ≥1).

Table 88: Efficacy Results in Patients with Recurrent or Metastatic Cervical Cancer (CPS ≥1) in KEYNOTE-158
Endpoint | Intravenous Pembrolizumab 200 mg every 3 weeks n=77 [Median follow-up time of 11.7 months (range 0.6 to 22.7 months)]
Objective Response Rate
ORR (95% CI) | 14.3% (7.4, 24.1)
Complete response rate | 2.6%
Partial response rate | 11.7%
Duration of Response
Median in months (range) | NR (4.1, 18.6+) [Based on patients (n=11) with a response by independent review]
% with duration ≥6 months | 91%
+ Denotes ongoing response
NR = not reached

14.12 Hepatocellular Carcinoma

Previously Treated HCC

The efficacy of intravenous pembrolizumab was investigated in KEYNOTE-394 (NCT03062358), a multicenter, randomized, placebo-controlled, double-blind trial conducted in Asia in patients with Barcelona Clinic Liver Cancer (BCLC) Stage B or C HCC, who were previously treated with sorafenib or oxaliplatin-based chemotherapy and who were not amenable to or were refractory to local-regional therapy. Patients were also required to have Child-Pugh A liver function.

Patients with hepatitis B had treated controlled disease (HBV viral load <2000 IU/mL or <10^4 copies/mL). Patients with an autoimmune disease that required systemic therapy within 2 years of treatment or a medical condition that required immunosuppression were ineligible. Patients with hepatic encephalopathy, main branch portal venous invasion, clinically apparent ascites, or esophageal or gastric variceal bleeding within the last 6 months were also ineligible.

Randomization was stratified by prior treatment: sorafenib vs. oxaliplatin-based chemotherapy, macrovascular invasion, and etiology (active HBV vs. others (active HCV, non-infected)). Patients were randomized (2:1) to receive pembrolizumab 200 mg intravenously every 3 weeks or placebo.

Treatment with intravenous pembrolizumab continued until RECIST v1.1-defined progression of disease as determined by BICR, unacceptable toxicity, or a maximum of 24 months. Assessment of tumor status was performed every 6 weeks. The main efficacy outcome measure was OS. Additional efficacy outcome measures were PFS, ORR, and DoR, as assessed by BICR using RECIST v1.1, modified to follow a maximum of 10 target lesions and a maximum of 5 target lesions per organ.

The study enrolled 453 patients, and 360 (79%) had active hepatitis B. The population characteristics in patients with active hepatitis B were: median age of 52 years (range: 23 to 82), 16% age 65 or older; 86% male; 100% Asian; 42% ECOG PS of 0 and 58% ECOG PS of 1; 90% received prior sorafenib and 10% received prior oxaliplatin-based chemotherapy. Patient characteristics also included extrahepatic disease (77%), macrovascular invasion (10%), BCLC stage C (93%) and B (7%), and baseline AFP ≥200 ng/mL (57%).

KEYNOTE-394 demonstrated improved OS in patients with HCC secondary to hepatitis B randomized to intravenous pembrolizumab compared with placebo. Efficacy results are summarized in Table 89 and Figure 31.

Table 89: Efficacy Results in Patients with Hepatocellular Carcinoma in KEYNOTE-394
Endpoint | Intravenous Pembrolizumab 200 mg every 3 weeks n=236 | Placebo n=124
OS [Results at the pre-specified final OS analysis]
Number (%) of patients with events | 172 (73) | 105 (85)
Median in months (95% CI) | 13.9 (12.5, 17.9) | 13.0 (10.1, 15.6)
Hazard ratio [Based on the stratified Cox proportional hazard model] (95% CI) | 0.78 (0.61, 0.99)
PFS [Results at pre-specified interim OS analysis]
Number (%) of patients with events | 189 (80) | 108 (87)
Median in months (95% CI) | 2 (1.4, 2.7) | 2.3 (1.4, 2.8)
Hazard ratio (95% CI) | 0.78 (0.61, 1.00)
Objective Response Rate
ORR [Confirmed complete response or partial response] (95% CI) | 11% (7, 16) | 1.6% (0.2, 5.7)
Number (%) of complete responses | 2 (0.9%) | 1 (0.8%)
Number (%) of partial responses | 24 (10%) | 1 (0.8%)
Duration of Response | n=28 | n=2
Median in months [Based on Kaplan-Meier estimate] (range) | 23.9 (2.6+, 44.4+) | 5.6 (3.0+, 5.6)
+ Denotes ongoing response

Figure 31: Kaplan-Meier Curve for Overall Survival in KEYNOTE-394

14.13 Biliary Tract Cancer

The efficacy of intravenous pembrolizumab in combination with gemcitabine and cisplatin chemotherapy was investigated in KEYNOTE-966 (NCT04003636), a multicenter, randomized, double-blind, placebo-controlled trial that enrolled 1069 patients with locally advanced unresectable or metastatic BTC, who had not received prior systemic therapy in the advanced disease setting. Patients with autoimmune disease that required systemic therapy within 2 years of treatment or a medical condition that required immunosuppression were ineligible. Randomization was stratified by region (Asia vs. non-Asia), locally advanced versus metastatic, and site of origin (gallbladder, intrahepatic or extrahepatic cholangiocarcinoma).

Patients were randomized (1:1) to intravenous pembrolizumab 200 mg on Day 1 plus gemcitabine 1000 mg/m^2 and cisplatin 25 mg/m^2 on Day 1 and Day 8 every 3 weeks, or placebo on Day 1 plus gemcitabine 1000 mg/m^2 and cisplatin 25 mg/m^2 on Day 1 and Day 8 every 3 weeks. Study medications were administered via intravenous infusion. Treatment continued until unacceptable toxicity or disease progression. For pembrolizumab, treatment continued for a maximum of 35 cycles, or approximately 24 months. For gemcitabine, treatment could be continued beyond 8 cycles while for cisplatin, treatment could be administered for a maximum of 8 cycles.

Administration of intravenous pembrolizumab with chemotherapy was permitted beyond RECIST-defined disease progression if the patient was clinically stable and considered by the investigator to be deriving clinical benefit. Assessment of tumor status was performed at baseline and then every 6 weeks through 54 weeks, followed by every 12 weeks thereafter.

Study population characteristics were median age of 64 years (range: 23 to 85), 47% age 65 or older; 52% male; 49% White, 46% Asian, 1.3% Black or African American; 10% Hispanic or Latino; 46% ECOG PS of 0 and 54% ECOG PS of 1; 31% of patients had a history of hepatitis B infection, and 3% had a history of hepatitis C infection.

The major efficacy outcome measure was OS. Additional efficacy outcome measures were PFS, ORR and DoR as assessed by BICR according to RECIST v1.1, modified to follow a maximum of 10 target lesions and a maximum of 5 target lesions per organ.

Table 90 and Figure 32 summarize the efficacy results for KEYNOTE-966.

Table 90: Efficacy Results in KEYNOTE-966
Endpoint | Intravenous Pembrolizumab 200 mg every 3 weeks with gemcitabine/cisplatin n=533 | Placebo with gemcitabine/cisplatin n=536
OS [Results at the pre-specified final OS analysis]
Number of patients with event (%) | 414 (78%) | 443 (83%)
Median in months (95% CI) | 12.7 (11.5, 13.6) | 10.9 (9.9, 11.6)
Hazard ratio [Based on the stratified Cox proportional hazard model] (95% CI) | 0.83 (0.72, 0.95)
p-Value [One-sided p-Value based on a stratified log-rank test] | 0.0034
PFS [Results at pre-specified final analysis of PFS and ORR]
Number (%) of patients with event | 361 (68%) | 391 (73%)
Median in months (95% CI) | 6.5 (5.7, 6.9) | 5.6 (5.1, 6.6)
Hazard ratio (95% CI) | 0.86 (0.75, 1.00)
p-Value | NS
Objective Response Rate
ORR [Confirmed complete response or partial response] (95% CI) | 29% (25, 33) | 29% (25, 33)
Number (%) of complete responses | 11 (2.1%) | 7 (1.3%)
Number (%) of partial responses | 142 (27%) | 146 (27%)
p-Value [One-sided p-Value based on the stratified Miettinen and Nurminen analysis] | NS
Duration of Response | n=156 | n=152
Median in months [Based on Kaplan-Meier estimate] (95% CI) | 8.3 (6.9, 10.2) | 6.8 (5.7, 7.1)
NS = not significant

Figure 32: Kaplan-Meier Curve for Overall Survival in KEYNOTE-966

14.14 Merkel Cell Carcinoma

The efficacy of intravenous pembrolizumab was investigated in KEYNOTE-017 (NCT02267603) and KEYNOTE-913 (NCT03783078), two multicenter, non-randomized, open-label trials that enrolled 105 patients with recurrent locally advanced or metastatic MCC who had not received prior systemic therapy for their advanced disease. Patients with active autoimmune disease or a medical condition that required immunosuppression were ineligible.

Patients received intravenous pembrolizumab 2 mg/kg (KEYNOTE-017) or 200 mg (KEYNOTE-913) every 3 weeks until unacceptable toxicity or disease progression that was symptomatic, rapidly progressive, required urgent intervention, occurred with a decline in performance status, or was confirmed at least 4 weeks later with repeat imaging. Patients without disease progression were treated for up to 24 months.

The major efficacy outcome measures were ORR and DoR as assessed by BICR per RECIST v1.1.

Among the 105 patients enrolled, the median age was 73 years (range: 38 to 91), 79% were age 65 or older; 62% were male; 80% were White, race in 19% was unknown or missing, and 1% were Asian; 53% had ECOG PS of 0, and 47% had ECOG PS of 1. Thirteen percent had stage IIIB disease and 84% had stage IV. Seventy-six percent of patients had prior surgery and 51% had prior radiation therapy.

Efficacy results are summarized in Table 91.

Table 91: Efficacy Results in KEYNOTE-017 and KEYNOTE-913
Endpoint | KEYNOTE-017 Intravenous Pembrolizumab 2 mg/kg every 3 weeks n=50 | KEYNOTE-913 Intravenous Pembrolizumab 200 mg or 2 mg/kg every 3 weeks n=55
Objective Response Rate
ORR (95% CI) | 56% (41, 70) | 49% (35, 63)
Complete responses, n (%) | 12 (24%) | 9 (16%)
Partial responses, n (%) | 16 (32%) | 18 (33%)
Duration of Response | n=28 | n=27
Median DoR in months (range) | NR (5.9, 34.5+) | NR (4.8, 25.4+)
Patients with duration ≥6 months, n (%) | 27 (96%) | 25 (93%)
Patients with duration ≥12 months, n (%) | 15 (54%) | 19 (70%)
+ Denotes ongoing response
NR = not reached

14.15 Renal Cell Carcinoma

First-line treatment with axitinib

KEYNOTE-426

The efficacy of intravenous pembrolizumab in combination with axitinib was investigated in KEYNOTE-426 (NCT02853331), a randomized, multicenter, open-label trial conducted in 861 patients who had not received systemic therapy for advanced RCC. Patients were enrolled regardless of PD-L1 tumor expression status. Patients with active autoimmune disease requiring systemic immunosuppression within the last 2 years were ineligible. Randomization was stratified by International Metastatic RCC Database Consortium (IMDC) risk categories (favorable versus intermediate versus poor) and geographic region (North America versus Western Europe versus “Rest of the World”).

Patients were randomized (1:1) to one of the following treatment arms:

- Intravenous pembrolizumab 200 mg intravenously every 3 weeks up to 24 months in combination with axitinib 5 mg orally, twice daily. Patients who tolerated axitinib 5 mg twice daily for 2 consecutive cycles (6 weeks) could increase to 7 mg and then subsequently to 10 mg twice daily. Axitinib could be interrupted or reduced to 3 mg twice daily and subsequently to 2 mg twice daily to manage toxicity.
- Sunitinib 50 mg orally, once daily for 4 weeks and then off treatment for 2 weeks.

Treatment with intravenous pembrolizumab and axitinib continued until RECIST v1.1-defined progression of disease or unacceptable toxicity. Administration of intravenous pembrolizumab and axitinib was permitted beyond RECIST-defined disease progression if the patient was clinically stable and considered to be deriving clinical benefit by the investigator. Assessment of tumor status was performed at baseline, after randomization at Week 12, then every 6 weeks thereafter until Week 54, and then every 12 weeks thereafter.

The study population characteristics were: median age of 62 years (range: 26 to 90), 38% age 65 or older; 73% male; 79% White and 16% Asian; 20% and 80% of patients had a baseline KPS of 70 to 80 and 90 to 100, respectively; and patient distribution by IMDC risk categories was 31% favorable, 56% intermediate, and 13% poor.

The main efficacy outcome measures were OS and PFS as assessed by BICR according to RECIST v1.1, modified to follow a maximum of 10 target lesions and a maximum of 5 target lesions per organ. Additional efficacy outcome measures included ORR, as assessed by BICR. A statistically significant improvement in OS was demonstrated at the first pre-specified interim analysis in patients randomized to intravenous pembrolizumab in combination with axitinib compared with sunitinib. The trial also demonstrated statistically significant improvements in PFS and ORR. An updated OS analysis was conducted when 418 deaths were observed based on the planned number of deaths for the pre-specified final analysis. Table 92 and Figure 33 summarize the efficacy results for KEYNOTE-426.

Table 92: Efficacy Results in KEYNOTE-426
Endpoint | Intravenous Pembrolizumab 200 mg every 3 weeks and Axitinib n=432 | Sunitinib n=429
Endpoint | OS
Number of patients with event (%) | 59 (14%) | 97 (23%)
Median in months (95% CI) | NR (NR, NR) | NR (NR, NR)
Hazard ratio [Based on the stratified Cox proportional hazard model] (95% CI) | 0.53 (0.38, 0.74)
p-Value [Based on stratified log-rank test] | <0.0001 [p-Value (one-sided) is compared with the allocated alpha of 0.0001 for this interim analysis (with 39% of the planned number of events for final analysis).]
Updated OS
Number of patients with event (%) | 193 (45%) | 225 (52%)
Median in months (95% CI) | 45.7 (43.6, NR) | 40.1 (34.3, 44.2)
Hazard ratio (95% CI) | 0.73 (0.60, 0.88)
PFS
Number of patients with event (%) | 183 (42%) | 213 (50%)
Median in months (95% CI) | 15.1 (12.6, 17.7) | 11.0 (8.7, 12.5)
Hazard ratio (95% CI) | 0.69 (0.56, 0.84)
p-Value | 0.0001 [p-Value (one-sided) is compared with the allocated alpha of 0.0013 for this interim analysis (with 81% of the planned number of events for final analysis).]
Objective Response Rate
ORR [Response: Best objective response as confirmed complete response or partial response] (95% CI) | 59% (54, 64) | 36% (31, 40)
Complete response rate | 6% | 2%
Partial response rate | 53% | 34%
p-Value [Based on Miettinen and Nurminen method stratified by IMDC risk group and geographic region] | <0.0001
NR = not reached

Figure 33: Kaplan-Meier Curve for Updated Overall Survival in KEYNOTE-426

In an exploratory analysis, the updated analysis of OS in patients with IMDC favorable, intermediate, intermediate/poor, and poor risk demonstrated a HR of 1.17 (95% CI: 0.76, 1.80), 0.67 (95% CI: 0.52, 0.86), 0.64 (95% CI: 0.52, 0.80), and 0.51 (95% CI: 0.32, 0.81), respectively.

First-line treatment with lenvatinib

KEYNOTE-581

The efficacy of intravenous pembrolizumab in combination with lenvatinib was investigated in KEYNOTE-581 (NCT02811861), a multicenter, open-label, randomized trial conducted in 1069 patients with advanced RCC in the first-line setting. Patients were enrolled regardless of PD-L1 tumor expression status. Patients with active autoimmune disease or a medical condition that required immunosuppression were ineligible. Randomization was stratified by geographic region (North America versus Western Europe versus “Rest of the World”) and Memorial Sloan Kettering Cancer Center (MSKCC) prognostic groups (favorable versus intermediate versus poor risk).

Patients were randomized (1:1:1) to one of the following treatment arms:

- Intravenous pembrolizumab 200 mg intravenously every 3 weeks up to 24 months in combination with lenvatinib 20 mg orally once daily.
- Lenvatinib 18 mg orally once daily in combination with everolimus 5 mg orally once daily.
- Sunitinib 50 mg orally once daily for 4 weeks then off treatment for 2 weeks.

Treatment continued until unacceptable toxicity or disease progression. Administration of intravenous pembrolizumab with lenvatinib was permitted beyond RECIST-defined disease progression if the patient was clinically stable and considered by the investigator to be deriving clinical benefit. intravenous pembrolizumab was continued for a maximum of 24 months; however, treatment with lenvatinib could be continued beyond 24 months. Assessment of tumor status was performed at baseline and then every 8 weeks.

The study population characteristics were: median age of 62 years (range: 29 to 88 years), 42% age 65 or older; 75% male; 74% White, 21% Asian, 1% Black, and 2% other races; 18% and 82% of patients had a baseline KPS of 70 to 80 and 90 to 100, respectively; patient distribution by MSKCC risk categories was 27% favorable, 64% intermediate, and 9% poor. Common sites of metastases in patients were lung (68%), lymph node (45%), and bone (25%).

The major efficacy outcome measures were PFS, as assessed by independent radiologic review (IRC) according to RECIST v1.1, and OS. Additional efficacy outcome measures included confirmed ORR as assessed by IRC. intravenous pembrolizumab in combination with lenvatinib demonstrated statistically significant improvements in PFS, OS, and ORR compared with sunitinib. An updated OS analysis was conducted when 304 deaths were observed based on the planned number of deaths for the pre-specified final analysis. Table 93 and Figures 34 and 35 summarize the efficacy results for KEYNOTE-581.

Table 93: Efficacy Results in KEYNOTE-581
Endpoint | Intravenous Pembrolizumab 200 mg every 3 weeks and Lenvatinib n=355 | Sunitinib n=357
Endpoint | Progression-Free Survival (PFS)
Number of events, n (%) | 160 (45%) | 205 (57%)
Progressive disease | 145 (41%) | 196 (55%)
Death | 15 (4%) | 9 (3%)
Median PFS in months (95% CI) | 23.9 (20.8, 27.7) | 9.2 (6.0, 11.0)
Hazard ratio [Hazard ratio is based on a Cox Proportional Hazards Model. Stratified by geographic region and MSKCC prognostic groups.] (95% CI) | 0.39 (0.32, 0.49)
p-Value [Two-sided p-Value based on stratified log-rank test.] | <0.0001
Overall Survival (OS)
Number of deaths, n (%) | 80 (23%) | 101 (28%)
Median OS in months (95% CI) | NR (33.6, NR) | NR (NR, NR)
Hazard ratio (95% CI) | 0.66 (0.49, 0.88)
p-Value | 0.0049
Updated OS
Number of deaths, n (%) | 149 (42%) | 159 (45%)
Median OS in months (95% CI) | 53.7 (48.7, NR) | 54.3 (40.9, NR)
Hazard ratio (95% CI) | 0.79 (0.63, 0.99)
Objective Response Rate (Confirmed)
ORR, n (%) | 252 (71%) | 129 (36%)
(95% CI) | (66, 76) | (31, 41)
Complete response rate | 16% | 4%
Partial response rate | 55% | 32%
p-Value [Two-sided p-Value based upon CMH test.] | <0.0001
Tumor assessments were based on RECIST 1.1; only confirmed responses are included for ORR.
Data cutoff date = 28 Aug 2020, Updated OS cutoff date = 31 July 2022
CI = confidence interval; NR= Not reached

Figure 34: Kaplan-Meier Curve for PFS in KEYNOTE-581

Figure 35: Kaplan-Meier Curve for Updated Overall Survival in KEYNOTE-581

KEYNOTE-B61

The efficacy of intravenous pembrolizumab in combination with lenvatinib was investigated in KEYNOTE-B61 (NCT04704219), a multicenter, single-arm trial that enrolled 160 patients with advanced or metastatic non-clear cell RCC in the first-line setting. Patients with active autoimmune disease or a medical condition that required immunosuppression were ineligible.

Patients received intravenous pembrolizumab 400 mg every 6 weeks in combination with lenvatinib 20 mg orally once daily. Intravenous pembrolizumab was continued for a maximum of 24 months; however, lenvatinib could be continued beyond 24 months. Treatment continued until unacceptable toxicity or disease progression. Administration of intravenous pembrolizumab with lenvatinib was permitted beyond RECIST-defined disease progression if the patient was considered by the investigator to be deriving clinical benefit.

Among the 158 treated patients, the baseline characteristics were: median age of 60 years (range: 24 to 87 years); 71% male; 86% White, 8% Asian, and 3% Black; <1% Hispanic or Latino; 22% and 78% of patients had a baseline KPS of 70 to 80 and 90 to 100, respectively; histologic subtypes were 59% papillary, 18% chromophobe, 4% translocation, <1% medullary, 13% unclassified, and 6% other; patient distribution by IMDC risk categories was 35% favorable, 54% intermediate, and 10% poor. Common sites of metastases in patients were lymph node (65%), lung (35%), bone (30%), and liver (21%).

The major efficacy outcome measure was ORR as assessed by BICR using RECIST 1.1. Additional efficacy outcome measures included DOR as assessed by BICR using RECIST 1.1. Efficacy results are summarized in Table 94.

Table 94: Efficacy Results in KEYNOTE-B61
Endpoint | Intravenous Pembrolizumab 400 mg every 6 weeks and Lenvatinib n=158
Objective Response Rate (Confirmed)
ORR (95% CI) | 51% (43, 59)
Complete response | 8%
Partial response | 42%
Duration of Response [Based on Kaplan-Meier estimates]
Median in months (range) | 19.5 (1.5+, 23.5+)
CI = confidence interval
+ Denotes ongoing response

Adjuvant Treatment of RCC (KEYNOTE-564)

The efficacy of intravenous pembrolizumab was investigated as adjuvant therapy for RCC in KEYNOTE-564 (NCT03142334), a multicenter, randomized (1:1), double-blind, placebo-controlled trial in 994 patients with intermediate-high or high risk of recurrence of RCC, or M1 no evidence of disease (NED). The intermediate-high risk category included: pT2 with Grade 4 or sarcomatoid features; pT3, any Grade without nodal involvement (N0) or distant metastases (M0). The high risk category included: pT4, any Grade N0 and M0; any pT, any Grade with nodal involvement and M0. The M1 NED category included patients with metastatic disease who had undergone complete resection of primary and metastatic lesions. Patients must have undergone a partial nephroprotective or radical complete nephrectomy (and complete resection of solid, isolated, soft tissue metastatic lesion(s) in M1 NED participants) with negative surgical margins ≥4 weeks prior to the time of screening. Patients were excluded from the trial if they had received prior systemic therapy for advanced RCC. Patients with active autoimmune disease or a medical condition that required immunosuppression were also ineligible. Patients were randomized to intravenous pembrolizumab 200 mg administered intravenously every 3 weeks or placebo for up to 1 year until disease recurrence or unacceptable toxicity. Randomization was stratified by metastasis status (M0, M1 NED); M0 group was further stratified by ECOG PS (0,1) and geographic region (US, non-US).

The study population characteristics were: median age of 60 years (range: 25 to 84), 33% age 65 or older; 71% male; 75% White, 14% Asian, 9% Unknown, 1% Black or African American, 1% American Indian or Alaska Native, 1% Multiracial; 13% Hispanic or Latino, 78% Not Hispanic or Latino, 8% Unknown; and 85% ECOG PS of 0 and 15% ECOG PS of 1. Ninety-four percent of patients enrolled had N0 disease; 11% had sarcomatoid features; 86% were intermediate-high risk; 8% were high risk; and 6% were M1 NED. Ninety-two percent of patients had a radical nephrectomy, and 8% had a partial nephrectomy.

The major efficacy outcome measure was investigator-assessed disease-free survival (DFS), defined as time to recurrence, metastasis, or death. An additional outcome measure was OS. Statistically significant improvements in DFS and OS were demonstrated at pre-specified interim analyses in patients randomized to the intravenous pembrolizumab arm compared with placebo. Efficacy results are summarized in Table 95 and Figures 36 and 37.

Table 95: Efficacy Results in KEYNOTE-564
Endpoint | Intravenous Pembrolizumab 200 mg every 3 weeks n=496 | Placebo n=498
DFS
Number (%) of patients with event | 109 (22%) | 151 (30%)
Median in months (95% CI) | NR | NR
Hazard ratio [Based on the stratified Cox proportional hazard model] (95% CI) | 0.68 (0.53, 0.87)
p-Value [Based on stratified log-rank test] | 0.0010 [p-Value (one-sided) is compared with a boundary of 0.0114.]
24-month DFS rate (95% CI) | 77% (73, 81) | 68% (64, 72)
OS
Number (%) of patients with event | 55 (11%) | 86 (17%)
Median in months (95% CI) | NR (NR, NR) | NR (NR, NR)
Hazard ratio (95% CI) | 0.62 (0.44, 0.87)
p-Value | 0.0024 [p-Value (one-sided) is compared with a boundary of 0.0072.]
48-month OS rate (95% CI) | 91% (88, 93) | 86% (83, 89)
NR = not reached

Figure 36: Kaplan-Meier Curve for Disease-Free Survival in KEYNOTE-564

Figure 37: Kaplan-Meier Curve for Overall Survival in KEYNOTE-564

14.16 Endometrial Carcinoma

In Combination with Paclitaxel and Carboplatin for the Treatment of Primary Advanced or Recurrent Endometrial Carcinoma

The efficacy of intravenous pembrolizumab in combination with paclitaxel and carboplatin was investigated in KEYNOTE-868/NRG-GY018 (NCT03914612), a multicenter, randomized, double-blind, placebo-controlled trial in 810 patients with advanced or recurrent endometrial carcinoma. The study design included two separate cohorts based on MMR status; 222 (27%) patients were in dMMR cohort, 588 (73%) patients were in pMMR cohort. The trial enrolled measurable Stage III, measurable Stage IVA, Stage IVB or recurrent endometrial cancer (with or without measurable disease). Patients who had not received prior systemic therapy or had received prior chemotherapy in the adjuvant setting were eligible. Patients who had received prior adjuvant chemotherapy were only eligible if their chemotherapy-free interval was at least 12 months. Patients with endometrial sarcoma, including carcinosarcoma, or patients with active autoimmune disease or a medical condition that required immunosuppression were ineligible. Randomization was stratified according to MMR status, ECOG PS (0 or 1 vs. 2), and prior adjuvant chemotherapy.

Patients were randomized (1:1) to one of the following treatment arms:

- Intravenous pembrolizumab 200 mg every 3 weeks, paclitaxel 175 mg/m^2 and carboplatin AUC 5 mg/mL/min for 6 cycles, followed by intravenous pembrolizumab 400 mg every 6 weeks for up to 14 cycles.
- Placebo every 3 weeks, paclitaxel 175 mg/m^2 and carboplatin AUC 5 mg/mL/min for 6 cycles, followed by placebo every 6 weeks for up to 14 cycles.

All study medications were administered as an intravenous infusion on Day 1 of each treatment cycle. Treatment continued until disease progression, unacceptable toxicity, or a maximum of 20 cycles (up to approximately 24 months). Patients with measurable disease who had RECIST-defined stable disease or partial response at the completion of cycle 6 were permitted to continue receiving paclitaxel and carboplatin with intravenous pembrolizumab or placebo for up to 10 cycles as determined by the investigator. Assessment of tumor status was performed every 9 weeks for the first 9 months and then every 12 weeks thereafter. The major efficacy outcome measure was PFS as assessed by the investigator according to RECIST 1.1. An additional efficacy outcome measure was OS.

The dMMR population characteristics were: median age of 66 years (range: 37 to 86), 55% age 65 or older; 79% White, 9% Black, and 3% Asian; 5% Hispanic or Latino; 64% ECOG PS of 0, 33% ECOG PS of 1, and 3% ECOG PS of 2; 61% had recurrent disease and 39% had primary or persistent disease; 5% received prior adjuvant chemotherapy and 43% received prior radiotherapy. The histologic subtypes were endometrioid carcinoma (81%), adenocarcinoma NOS (11%), serous carcinoma (2%), and other (6%).

The pMMR population characteristics were: median age of 66 years (range: 29 to 94), 54% age 65 or older; 72% White, 16% Black, and 5% Asian; 6% Hispanic or Latino; 67% ECOG PS of 0, 30% ECOG PS of 1, and 3% ECOG PS of 2; 56% had recurrent disease and 44% had primary or persistent disease; 26% received prior adjuvant chemotherapy and 41% received prior radiotherapy. The histologic subtypes were endometrioid carcinoma (52%), serous carcinoma (26%), adenocarcinoma NOS (10%), clear cell carcinoma (7%), and other (5%).

The trial demonstrated statistically significant improvements in PFS for patients randomized to intravenous pembrolizumab in combination with paclitaxel and carboplatin compared to placebo in combination with paclitaxel and carboplatin in both the dMMR and pMMR populations. Table 96 and Figures 38 and 39 summarize the efficacy results for KEYNOTE-868 by MMR status. At the time of the PFS analysis, OS data were not mature with 12% deaths in the dMMR population and 17% deaths in the pMMR population.

Table 96: Efficacy Results in KEYNOTE-868
Endpoint | dMMR Population |  | pMMR Population
Endpoint | Intravenous Pembrolizumab with paclitaxel and carboplatin n=110 | Placebo with paclitaxel and carboplatin n=112 | Intravenous Pembrolizumab with paclitaxel and carboplatin n=294 | Placebo with paclitaxel and carboplatin n=294
PFS [Based on interim PFS analysis; the information fractions for interim analyses were 49% for dMMR and 55% for pMMR.]
Number (%) of patients with event | 26 (24%) | 57 (51%) | 91 (31%) | 124 (42%)
Median in months (95% CI) | NR (30.7, NR) | 6.5 (6.4, 8.7) | 11.1 (8.7, 13.5) | 8.5 (7.2, 8.8)
Hazard ratio [Based on the stratified Cox proportional hazard model] (95% CI) | 0.30 (0.19, 0.48) |  | 0.60 (0.46, 0.78)
p-Value [Based on the stratified log-rank test] | <0.0001 |  | <0.0001
NR = not reached

Figure 38: Kaplan-Meier Curve for Progression-Free Survival in KEYNOTE-868 (dMMR Population)

Figure 39: Kaplan-Meier Curve for Progression-Free Survival in KEYNOTE-868 (pMMR Population)

Lack of Effectiveness for Adjuvant Treatment of Patients with Endometrial Carcinoma

The efficacy of intravenous pembrolizumab in combination with carboplatin and paclitaxel, with or without radiation, was investigated in KEYNOTE‑B21 (NCT04634877), a randomized, multicenter, double-blind, placebo-controlled trial in 1,095 patients with newly-diagnosed, high‑risk endometrial cancer with no evidence of disease on imaging following curative intent surgery. High-risk disease was defined as any of the following (staging per FIGO 2009): Stage I/II with myometrial invasion and either non-endometrioid histology or aberrant p53 expression or p53 mutation, or Stage III/IVA. The trial did not meet the prespecified primary endpoint for investigator-assessed DFS, with a HR of 1.02 (95% CI: 0.79, 1.32).

In Combination with Lenvatinib for the Treatment of Advanced Endometrial Carcinoma That Is pMMR or Not MSI-H

The efficacy of intravenous pembrolizumab in combination with lenvatinib was investigated in KEYNOTE-775 (NCT03517449), a multicenter, open-label, randomized, active-controlled trial that enrolled 827 patients with advanced endometrial carcinoma who had been previously treated with at least one prior platinum-based chemotherapy regimen in any setting, including in the neoadjuvant and adjuvant settings. Patients with endometrial sarcoma, including carcinosarcoma, or patients who had active autoimmune disease or a medical condition that required immunosuppression were ineligible. Patients with endometrial carcinoma that were pMMR (using the VENTANA MMR RxDx Panel test) or not MSI-H were stratified by ECOG performance status, geographic region, and history of pelvic radiation. Patients were randomized (1:1) to one of the following treatment arms:

- Intravenous pembrolizumab 200 mg intravenously every 3 weeks in combination with lenvatinib 20 mg orally once daily.
- Investigator’s choice, consisting of either doxorubicin 60 mg/m^2 every 3 weeks or paclitaxel 80 mg/m^2 given weekly, 3 weeks on/1 week off.

Treatment with intravenous pembrolizumab and lenvatinib continued until RECIST v1.1-defined progression of disease as verified by BICR, unacceptable toxicity, or for intravenous pembrolizumab, a maximum of 24 months. Treatment was permitted beyond RECIST v1.1-defined disease progression if the treating investigator considered the patient to be deriving clinical benefit, and the treatment was tolerated. Assessment of tumor status was performed every 8 weeks. The major efficacy outcome measures were OS and PFS as assessed by BICR according to RECIST v1.1, modified to follow a maximum of 10 target lesions and a maximum of 5 target lesions per organ. Additional efficacy outcome measures included ORR and DoR, as assessed by BICR.

Among the 697 pMMR patients, 346 patients were randomized to intravenous pembrolizumab in combination with lenvatinib, and 351 patients were randomized to investigator’s choice of doxorubicin (n=254) or paclitaxel (n=97). The pMMR population characteristics were: median age of 65 years (range: 30 to 86), 52% age 65 or older; 62% White, 22% Asian, and 3% Black; 60% ECOG PS of 0 and 40% ECOG PS of 1. The histologic subtypes were endometrioid carcinoma (55%), serous (30%), clear cell carcinoma (7%), mixed (4%), and other (3%). All 697 of these patients received prior systemic therapy for endometrial carcinoma: 67% had one, 30% had two, and 3% had three or more prior systemic therapies. Thirty-seven percent of patients received only prior neoadjuvant or adjuvant therapy.

Efficacy results for the pMMR or not MSI-H patients are summarized in Table 97 and Figures 40 and 41.

Table 97: Efficacy Results in KEYNOTE-775
 | Endometrial Carcinoma (pMMR or not MSI-H)
Endpoint | Intravenous Pembrolizumab 200 mg every 3 weeks and Lenvatinib n=346 | Doxorubicin or Paclitaxel n=351
OS
Number (%) of patients with event | 165 (48%) | 203 (58%)
Median in months (95% CI) | 17.4 (14.2, 19.9) | 12.0 (10.8, 13.3)
Hazard ratio [Based on the stratified Cox regression model] (95% CI) | 0.68 (0.56, 0.84)
p-Value [Based on stratified log-rank test] | 0.0001
PFS
Number (%) of patients with event | 247 (71%) | 238 (68%)
Median in months (95% CI) | 6.6 (5.6, 7.4) | 3.8 (3.6, 5.0)
Hazard ratio (95% CI) | 0.60 (0.50, 0.72)
p-Value | <0.0001
Objective Response Rate
ORR [Response: Best objective response as confirmed complete response or partial response] (95% CI) | 30% (26, 36) | 15% (12, 19)
Complete response rate | 5% | 3%
Partial response rate | 25% | 13%
p-Value [Based on Miettinen and Nurminen method stratified by ECOG performance status, geographic region, and history of pelvic radiation] | <0.0001
Duration of Response | n=105 | n=53
Median in months (range) | 9.2 (1.6+, 23.7+) | 5.7 (0.0+, 24.2+)

Figure 40: Kaplan-Meier Curve for Overall Survival in KEYNOTE-775 (pMMR or Not MSI-H)

Figure 41: Kaplan-Meier Curve for Progression-Free Survival in KEYNOTE-775 (pMMR or Not MSI-H)

As a Single Agent for the Treatment of Advanced MSI-H or dMMR Endometrial Carcinoma

The efficacy of intravenous pembrolizumab was investigated in KEYNOTE-158 (NCT02628067), a multicenter, non-randomized, open-label, multi-cohort trial. The trial enrolled 90 patients with unresectable or metastatic MSI-H or dMMR endometrial carcinoma in Cohorts D and K. MSI or MMR tumor status was determined using polymerase chain reaction (PCR) or immunohistochemistry (IHC), respectively. Patients with autoimmune disease or a medical condition that required immunosuppression were ineligible. Patients received intravenous pembrolizumab 200 mg intravenously every 3 weeks until unacceptable toxicity or documented disease progression. Patients treated with intravenous pembrolizumab without disease progression could be treated for up to 24 months. Assessment of tumor status was performed every 9 weeks for the first 12 months, and every 12 weeks thereafter. The major efficacy outcome measures were ORR and DoR as assessed by BICR according to RECIST v1.1, modified to follow a maximum of 10 target lesions and a maximum of 5 target lesions per organ.

Among the 90 patients evaluated, the baseline characteristics were: median age of 64 years (range: 42 to 86); 83% White, 8% Asian, and 3% Black; 12% Hispanic or Latino; 39% ECOG PS of 0 and 61% ECOG PS of 1; 96% had M1 disease and 4% had M0 disease at study entry; and 51% had one and 48% had two or more prior lines of therapy. Nine patients received only adjuvant therapy and one patient received only neoadjuvant and adjuvant therapy before participating in the study.

Efficacy results are summarized in Table 98.

Table 98: Efficacy Results in Patients with Advanced MSI-H or dMMR Endometrial Carcinoma in KEYNOTE-158
Endpoint | Intravenous Pembrolizumab n=90 [Median follow-up time of 16.0 months (range 0.5 to 62.1 months)]
Objective Response Rate
ORR (95% CI) | 46% (35, 56)
Complete response rate | 12%
Partial response rate | 33%
Duration of Response | n=41
Median in months (range) | NR (2.9, 55.7+)
% with duration ≥12 months | 68%
% with duration ≥24 months | 44%
+ Denotes ongoing response
NR = not reached

14.17 Tumor Mutational Burden-High Cancer

The efficacy of intravenous pembrolizumab was investigated in a prospectively-planned retrospective analysis of 10 cohorts (A through J) of patients with various previously treated unresectable or metastatic solid tumors with high tumor mutation burden (TMB-H) who were enrolled in a multicenter, non-randomized, open-label trial, KEYNOTE-158 (NCT02628067). The trial excluded patients who previously received an anti-PD-1 or other immune-modulating monoclonal antibody, or who had an autoimmune disease, or a medical condition that required immunosuppression. Patients received intravenous pembrolizumab 200 mg intravenously every 3 weeks until unacceptable toxicity or documented disease progression. Assessment of tumor status was performed every 9 weeks for the first 12 months and every 12 weeks thereafter.

The statistical analysis plan pre-specified ≥10 and ≥13 mutations per megabase using the FoundationOne CDx assay as cutpoints to assess TMB. Testing of TMB was blinded with respect to clinical outcomes. The major efficacy outcome measures were ORR and DoR in patients who received at least one dose of intravenous pembrolizumab as assessed by BICR according to RECIST v1.1, modified to follow a maximum of 10 target lesions and a maximum of 5 target lesions per organ.

In KEYNOTE-158, 1050 patients were included in the efficacy analysis population. TMB was analyzed in the subset of 790 patients with sufficient tissue for testing based on protocol-specified testing requirements. Of the 790 patients, 102 (13%) had tumors identified as TMB-H, defined as TMB ≥10 mutations per megabase. Among the 102 patients with TMB-H advanced solid tumors, the study population characteristics were: median age of 61 years (range: 27 to 80), 34% age 65 or older; 34% male; 81% White; and 41% ECOG PS of 0 and 58% ECOG PS of 1. Fifty-six percent of patients had at least two prior lines of therapy.

Efficacy results are summarized in Tables 99 and 100.

Table 99: Efficacy Results for Patients with TMB-H Cancer in KEYNOTE-158
Endpoint | Intravenous Pembrolizumab 200 mg every 3 weeks
 | TMB ≥10 mut/Mb n=102 [Median follow-up time of 11.1 months] | TMB ≥13 mut/Mb n=70
Objective Response Rate
ORR (95% CI) | 29% (21, 39) | 37% (26, 50)
Complete response rate | 4% | 3%
Partial response rate | 25% | 34%
Duration of Response | n=30 | n=26
Median in months (range) [From product-limit (Kaplan-Meier) method for censored data] | NR (2.2+, 34.8+) | NR (2.2+, 34.8+)
% with duration ≥12 months | 57% | 58%
% with duration ≥24 months | 50% | 50%
+ Denotes ongoing response
NR = not reached

Table 100: Response by Tumor Type (TMB ≥10 mut/Mb)
 |  | Objective Response Rate |  | Duration of Response range
 | N | n (%) | 95% CI | (months)
Overall [No TMB-H patients were identified in the cholangiocarcinoma cohort] | 102 | 30 (29%) | (21%, 39%) | (2.2+, 34.8+)
Small cell lung cancer | 34 | 10 (29%) | (15%, 47%) | (4.1, 32.5+)
Cervical cancer | 16 | 5 (31%) | (11%, 59%) | (3.7+, 34.8+)
Endometrial cancer | 15 | 7 (47%) | (21%, 73%) | (8.4+, 33.9+)
Anal cancer | 14 | 1 (7%) | (0.2%, 34%) | 18.8+
Vulvar cancer | 12 | 2 (17%) | (2%, 48%) | (8.8, 11.0)
Neuroendocrine cancer | 5 | 2 (40%) | (5%, 85%) | (2.2+, 32.6+)
Salivary cancer | 3 | PR, SD, PD |  | 31.3+
Thyroid cancer | 2 | CR, CR |  | (8.2, 33.2+)
Mesothelioma cancer | 1 | PD
CR = complete response
PR = partial response
SD = stable disease
PD = progressive disease

In an exploratory analysis in 32 patients enrolled in KEYNOTE-158 whose cancer had TMB ≥10 mut/Mb and <13 mut/Mb, the ORR was 13% (95% CI: 4%, 29%), including two complete responses and two partial responses.

14.18 Cutaneous Squamous Cell Carcinoma

The efficacy of intravenous pembrolizumab was investigated in patients with recurrent or metastatic cSCC or locally advanced cSCC enrolled in KEYNOTE-629 (NCT03284424), a multicenter, multi-cohort, non-randomized, open-label trial. The trial excluded patients with autoimmune disease or a medical condition that required immunosuppression.

Patients received intravenous pembrolizumab 200 mg intravenously every 3 weeks until documented disease progression, unacceptable toxicity, or a maximum of 24 months. Patients with initial radiographic disease progression could receive additional doses of intravenous pembrolizumab during confirmation of progression unless disease progression was symptomatic, rapidly progressive, required urgent intervention, or occurred with a decline in performance status.

Assessment of tumor status was performed every 6 weeks during the first year, and every 9 weeks during the second year. The major efficacy outcome measures were ORR and DoR as assessed by BICR according to RECIST v1.1, modified to follow a maximum of 10 target lesions and a maximum of 5 target lesions per organ.

Among the 105 patients with recurrent or metastatic cSCC treated, the study population characteristics were: median age of 72 years (range: 29 to 95), 71% age 65 or older; 76% male; 70% White, 25% race unknown; 34% ECOG PS of 0 and 66% ECOG PS of 1. Forty-five percent of patients had locally recurrent only cSCC, 24% had metastatic only cSCC, and 31% had both locally recurrent and metastatic cSCC. Eighty-seven percent received one or more prior lines of therapy; 73% received prior radiation therapy.

Among the 54 patients with locally advanced cSCC treated, the study population characteristics were: median age of 76 years (range: 35 to 95), 80% age 65 or older; 72% male; 83% White, 13% race unknown; 41% ECOG PS of 0 and 59% ECOG PS of 1. Twenty-two percent received one or more prior lines of therapy; 63% received prior radiation therapy.

Efficacy results are summarized in Table 101.

Table 101: Efficacy Results in KEYNOTE-629
Endpoint | Intravenous Pembrolizumab Recurrent or Metastatic cSCC n=105 | Intravenous Pembrolizumab Locally Advanced cSCC n=54
Objective Response Rate
ORR (95% CI) | 35% (26, 45) | 52% (38, 66)
Complete response rate | 12% | 22%
Partial response rate | 23% | 30%
Duration of Response [Median follow-up time: recurrent or metastatic cSCC: 23.8 months; locally advanced cSCC: 48.0 months] | n=37 | n=28
Median in months (range) | NR (2.7, 64.2+) | 47.2 (1.0+, 49.9+)
% with duration ≥6 months | 76% | 89%
% with duration ≥12 months | 68% | 75%
+ Denotes ongoing response

14.19 Triple-Negative Breast Cancer

Neoadjuvant and Adjuvant Treatment of High-Risk Early-Stage TNBC

The efficacy of intravenous pembrolizumab in combination with neoadjuvant chemotherapy followed by surgery and continued adjuvant treatment with intravenous pembrolizumab as a single agent was investigated in KEYNOTE-522 (NCT03036488), a randomized (2:1), multicenter, double-blind, placebo-controlled trial conducted in 1174 patients with newly diagnosed previously untreated high-risk early-stage TNBC (tumor size >1 cm but ≤2 cm in diameter with nodal involvement or tumor size >2 cm in diameter regardless of nodal involvement). Patients were enrolled regardless of tumor PD-L1 expression. Patients with active autoimmune disease that required systemic therapy within two years of treatment or a medical condition that required immunosuppression were ineligible. Randomization was stratified by nodal status (positive vs. negative), tumor size (T1/T2 vs. T3/T4), and choice of carboplatin (dosed every 3 weeks vs. weekly).

Patients were randomized (2:1) to one of the following two treatment arms; all study medications were administered intravenously:

- Arm 1:
  - Four cycles of preoperative intravenous pembrolizumab 200 mg every 3 weeks on Day 1 of cycles 1-4 of treatment regimen in combination with:
    - Carboplatin
      - AUC 5 mg/mL/min every 3 weeks on Day 1 of cycles 1-4 of treatment regimen
        -or-
      - AUC 1.5 mg/mL/min every week on Days 1, 8, and 15 of cycles 1-4 of treatment regimen
        -and-
    - Paclitaxel 80 mg/m^2 every week on Days 1, 8, and 15 of cycles 1-4 of treatment regimen
  - Followed by four additional cycles of preoperative intravenous pembrolizumab 200 mg every 3 weeks on Day 1 of cycles 5-8 of treatment regimen in combination with:
    - Doxorubicin 60 mg/m^2 -or- epirubicin 90 mg/m^2 every 3 weeks on Day 1 of cycles 5-8 of treatment regimen -and-
    - Cyclophosphamide 600 mg/m^2 every 3 weeks on Day 1 of cycles 5-8 of treatment regimen
  - Following surgery, nine cycles of intravenous pembrolizumab 200 mg every 3 weeks were administered.
- Arm 2:
  - Four cycles of preoperative placebo every 3 weeks on Day 1 of cycles 1-4 of treatment regimen in combination with:
    - Carboplatin
      - AUC 5 mg/mL/min every 3 weeks on Day 1 of cycles 1-4 of treatment regimen
        -or-
      - AUC 1.5 mg/mL/min every week on Days 1, 8, and 15 of cycles 1-4 of treatment regimen
        -and-
    - Paclitaxel 80 mg/m^2 every week on Days 1, 8, and 15 of cycles 1-4 of treatment regimen
  - Followed by four cycles of preoperative placebo every 3 weeks on Day 1 of cycles 5-8 of treatment regimen in combination with:
    - Doxorubicin 60 mg/m^2 -or- epirubicin 90 mg/m^2 every 3 weeks on Day 1 of cycles 5-8 of treatment regimen -and-
    - Cyclophosphamide 600 mg/m^2 every 3 weeks on Day 1 of cycles 5-8 of treatment regimen
  - Following surgery, nine cycles of placebo every 3 weeks were administered.

The trial was not designed to isolate the effect of intravenous pembrolizumab in each phase (neoadjuvant or adjuvant) of treatment.

The main efficacy outcomes were pCR rate and EFS. pCR was defined as absence of invasive cancer in the breast and lymph nodes (ypT0/Tis ypN0) and was assessed by the blinded local pathologist at the time of definitive surgery. EFS was defined as the time from randomization to the first occurrence of any of the following events: progression of disease that precludes definitive surgery, local or distant recurrence, second primary malignancy, or death due to any cause. An additional efficacy outcome was overall survival (OS).

The study population characteristics were: median age of 49 years (range: 22 to 80), 11% age 65 or older; 99.9% female; 64% White, 20% Asian, 4.5% Black, and 1.8% American Indian or Alaska Native; 87% ECOG PS of 0 and 13% ECOG PS of 1; 56% were pre-menopausal status and 44% were post-menopausal status; 7% were primary Tumor 1 (T1), 68% T2, 19% T3, and 7% T4; 49% were nodal involvement 0 (N0), 40% N1, 11% N2, and 0.2% N3; 75% of patients were overall Stage II and 25% were Stage III.

Statistically significant improvements in pCR, EFS, and OS were demonstrated at pre-specified interim analyses for patients randomized to intravenous pembrolizumab in combination with chemotherapy followed by intravenous pembrolizumab as a single agent compared with patients randomized to placebo in combination with chemotherapy followed by placebo alone.

Table 102 and Figures 42 and 43 summarize the efficacy results for KEYNOTE-522.

Table 102: Efficacy Results in KEYNOTE-522
Endpoint | Intravenous Pembrolizumab 200 mg every 3 weeks with chemotherapy/Intravenous Pembrolizumab n=784 | Placebo with chemotherapy/Placebo n=390
pCR (ypT0/Tis ypN0) [Based on the entire intention-to-treat population n=1174 patients]
Number of patients with pCR | 494 | 217
pCR rate (%), (95% CI) | 63.0 (59.5, 66.4) | 55.6 (50.6, 60.6)
Treatment difference (%) estimate (95% CI) [Based on a pre-specified pCR interim analysis in n=602 patients, the pCR rate difference was statistically significant (p=0.00055 compared to a significance level of 0.003).] , [Based on Miettinen and Nurminen method stratified by nodal status, tumor size, and choice of carboplatin] | 7.5 (1.6, 13.4)
EFS
Number of patients with event (%) | 123 (16%) | 93 (24%)
Hazard ratio (95% CI) [Based on stratified Cox regression model] | 0.63 (0.48, 0.82)
p-Value [Based on a pre-specified EFS interim analysis (compared to a significance level of 0.0052)] , [Based on log-rank test stratified by nodal status, tumor size, and choice of carboplatin] | 0.00031
OS
Number of patients with event (%) | 115 (15%) | 85 (22%)
Hazard ratio (95% CI) | 0.66 (0.50, 0.87)
p-Value, [Based on a pre-specified OS interim analysis (compared to a significance level of 0.0050)] | 0.00150

Figure 42: Kaplan-Meier Curve for Event-Free Survival in KEYNOTE-522

Figure 43: Kaplan-Meier Curve for Overall Survival in KEYNOTE-522

Locally Recurrent Unresectable or Metastatic TNBC for Tumors Expressing PD-L1 (CPS≥ 10)

The efficacy of intravenous pembrolizumab in combination with paclitaxel, paclitaxel protein-bound, or gemcitabine and carboplatin was investigated in KEYNOTE-355 (NCT02819518), a multicenter, double-blind, randomized, placebo-controlled trial conducted in 847 patients with locally recurrent unresectable or metastatic TNBC, regardless of tumor PD-L1 expression, who had not been previously treated with chemotherapy in the metastatic setting. Patients with active autoimmune disease that required systemic therapy within 2 years of treatment or a medical condition that required immunosuppression were ineligible. Randomization was stratified by chemotherapy treatment (paclitaxel or paclitaxel protein-bound vs. gemcitabine and carboplatin), tumor PD-L1 expression (CPS ≥1 vs. CPS <1) according to the PD-L1 IHC 22C3 pharmDx assay, and prior treatment with the same class of chemotherapy in the neoadjuvant setting (yes vs. no).

Patients were randomized (2:1) to one of the following treatment arms; all study medications were administered via intravenous infusion:

- Intravenous pembrolizumab 200 mg on Day 1 every 3 weeks in combination with paclitaxel protein-bound 100 mg/m^2 on Days 1, 8 and 15 every 28 days, paclitaxel 90 mg/m^2 on Days 1, 8, and 15 every 28 days, or gemcitabine 1000 mg/m^2 and carboplatin AUC 2 mg/mL/min on Days 1 and 8 every 21 days.
- Placebo on Day 1 every 3 weeks in combination with paclitaxel protein-bound 100 mg/m^2 on Days 1, 8 and 15 every 28 days, paclitaxel 90 mg/m^2 on Days 1, 8, and 15 every 28 days, or gemcitabine 1000 mg/m^2 and carboplatin AUC 2 mg/mL/min on Days 1 and 8 every 21 days.

Assessment of tumor status was performed at Weeks 8, 16, and 24, then every 9 weeks for the first year, and every 12 weeks thereafter. The main efficacy outcome measures were OS and PFS as assessed by BICR according to RECIST v1.1, modified to follow a maximum of 10 target lesions and a maximum of 5 target lesions per organ, tested in the subgroup of patients with CPS ≥10. Additional efficacy outcome measures were ORR and DoR as assessed by BICR.

The study population characteristics for patients were: median age of 53 years (range: 22 to 85), 21% age 65 or older; 100% female; 68% White, 21% Asian, and 4% Black; 60% ECOG PS of 0 and 40% ECOG PS of 1; and 68% were post-menopausal status. Seventy-five percent of patients had tumor PD-L1 expression CPS ≥1 and 38% had tumor PD-L1 expression CPS ≥10.

Table 103 and Figures 44 and 45 summarize the efficacy results for KEYNOTE-355.

Table 103: Efficacy Results in KEYNOTE-355 (CPS ≥10)
Endpoint | Intravenous Pembrolizumab 200 mg every 3 weeks with chemotherapy n=220 | Placebo every 3 weeks with chemotherapy n=103
OS [Based on the pre-specified final analysis]
Number of patients with event (%) | 155 (70%) | 84 (82%)
Median in months (95% CI) | 23 (19.0, 26.3) | 16.1 (12.6, 18.8)
Hazard ratio [Based on stratified Cox regression model] (95% CI) | 0.73 (0.55, 0.95)
p-Value [One-sided p-Value based on stratified log-rank test (compared to a significance level of 0.0113)] | 0.0093
PFS [Based on a pre-specified interim analysis]
Number of patients with event (%) | 136 (62%) | 79 (77%)
Median in months (95% CI) | 9.7 (7.6, 11.3) | 5.6 (5.3, 7.5)
Hazard ratio (95% CI) | 0.65 (0.49, 0.86)
p-Value [One-sided p-Value based on stratified log-rank test (compared to a significance level of 0.00411)] | 0.0012
Objective Response Rate (Confirmed)
ORR (95% CI) | 53% (46, 59) | 41% (31, 51)
Complete response rate | 17% | 14%
Partial response rate | 35% | 27%
Duration of Response | n=116 | n=42
Median in months (95% CI) | 12.8 (9.9, 25.9) | 7.3 (5.5, 15.4)

Figure 44: Kaplan-Meier Curve for Overall Survival in KEYNOTE-355 (CPS ≥10)

Figure 45: Kaplan-Meier Curve for Progression-Free Survival in KEYNOTE-355 (CPS ≥10)

14.20 Ovarian Cancer

The efficacy of intravenous pembrolizumab in combination with paclitaxel, with or without bevacizumab, was evaluated in KEYNOTE-B96 (NCT05116189), a multicenter, randomized, double-blind, placebo-controlled trial that enrolled 643 patients with platinum-resistant, epithelial ovarian, fallopian tube, or primary peritoneal carcinoma who received one or two prior lines of systemic therapy for ovarian carcinoma. Patients must have received at least one line of platinum-based chemotherapy for ovarian cancer with radiographic evidence of disease progression within 6 months after the last dose. Prior therapy with an anti-PD-1/PD-L1 inhibitor, PARP inhibitor, or bevacizumab was permitted. Patients were enrolled regardless of PD-L1 tumor expression status. Patients with autoimmune disease that required systemic therapy within 2 years of treatment or a medical condition that required immunosuppression were ineligible. Randomization was stratified by investigator decision to use bevacizumab, geographic region (U.S. or European Union or Rest of World), and PD-L1 status according to the PD-L1 IHC 22C3 pharmDx assay (CPS <1 or CPS 1 to <10 or CPS ≥10). Patients were randomized (1:1) to one of the two treatment groups:

- Intravenous pembrolizumab 400 mg every 6 weeks plus paclitaxel 80 mg/m^2 with or without bevacizumab 10 mg/kg
- Placebo every 6 weeks plus paclitaxel 80 mg/m^2 with or without bevacizumab 10 mg/kg

All study medications were administered as an intravenous infusion. Intravenous pembrolizumab 400 mg or placebo were administered on Day 1 of each 6-week treatment cycle and paclitaxel 80 mg/m^2 was administered on Days 1, 8, and 15 of each 3-week treatment cycle. The option to use bevacizumab was by investigator choice prior to randomization. Bevacizumab 10 mg/kg was administered on Day 1 of a 2-week treatment cycle. Treatment with intravenous pembrolizumab continued until RECIST v1.1-defined progression of disease, unacceptable toxicity, or a maximum of 24 months. Administration of intravenous pembrolizumab was permitted beyond RECIST-defined disease progression if the patient was clinically stable and considered to be deriving clinical benefit by the investigator. Assessment of tumor status was performed every 9 weeks for the first year, followed by every 12 weeks thereafter. The major efficacy outcome measure was PFS as assessed by investigator according to RECIST v1.1. An additional efficacy outcome measure was OS.

Among the 643 patients randomized, 466 patients (72%) had tumors expressing PD-L1 with a CPS ≥1. The population characteristics of these 466 patients were: median age of 62 years (range: 37 to 85), 38% age 65 or older; 67% White, 20% Asian, 8% Missing, 3% Multiple, 2% Black, 0.4% Native Hawaiian or other Pacific Islander; 13% Hispanic or Latino; 55% and 44% ECOG performance status of 0 or 1, respectively; 73% received bevacizumab as study treatment; 36% of patients had received one prior line and 64% had received two prior lines of therapy; prior systemic therapy included: 46% with bevacizumab; 39% with a PARP inhibitor, or 3% with an anti-PD-1/PD-L1 inhibitor. The platinum-free interval following the most recent line of therapy was <3 months in 47% of patients, and 3 to 6 months in 53% of patients.

The study demonstrated statistically significant improvement in PFS and OS for patients randomized to intravenous pembrolizumab in combination with paclitaxel with or without bevacizumab compared to placebo in combination with paclitaxel with or without bevacizumab in patients whose tumors expressed PD-L1 CPS ≥1. Efficacy results are summarized in Table 104 and Figures 46 and 47.

Table 104: Efficacy Results in KEYNOTE-B96 (CPS ≥1)
Endpoint | Intravenous pembrolizumab 400 mg every 6 weeks plus paclitaxel with or without bevacizumab n=234 | Placebo plus paclitaxel with or without bevacizumab n=232
PFS
Number of patients with event (%) | 162 (69) | 180 (78)
Median in months (95% CI) | 8.3 (7.0, 9.4) | 7.2 (6.2, 8.1)
Hazard ratio (95% CI) | 0.72 (0.58, 0.89)
p-Value | 0.0014 [Based on stratified log-rank test (p-Value [one-sided] is compared to an alpha boundary of 0.0116)]
OS
Number of patients with event (%) | 157 (67) | 175 (75)
Median in months (95% CI) | 18.2 (15.3, 21.0) | 14.0 (12.5, 16.1)
Hazard ratio (95% CI) | 0.76 (0.61, 0.94)
p-Value | 0.0053 [Based on stratified log-rank test (p-Value [one-sided] is compared to an alpha boundary of 0.0083)]

Figure 46: Kaplan-Meier Curve for Progression-Free Survival in KEYNOTE-B96 (CPS ≥1)

Figure 47: Kaplan-Meier Curve for Overall Survival in KEYNOTE-B96 (CPS ≥1)

16 HOW SUPPLIED/STORAGE AND HANDLING

KEYTRUDA QLEX (pembrolizumab and berahyaluronidase alfa-pmph) injection is a sterile, preservative-free, clear to slightly opalescent, colorless to slightly yellow solution supplied in single-dose vials for subcutaneous administration. Each carton contains one single-dose vial either as:

- 395 mg pembrolizumab and 4,800 units berahyaluronidase alfa per 2.4 mL (165 mg/ 2,000 units per mL), NDC 0006-3083-01
- 790 mg pembrolizumab and 9,600 units berahyaluronidase alfa per 4.8 mL (165 mg/ 2,000 units per mL), NDC 0006-5083-01

STORAGE AND HANDLING

Store vials refrigerated at 2°C to 8°C (36°F to 46°F) in original carton to protect from light. Do not freeze. Do not shake.

17 PATIENT COUNSELING INFORMATION

Advise the patient to read the FDA-authorized patient labeling (Medication Guide).

Immune-Mediated Adverse Reactions

- Inform patients of the risk of immune-mediated adverse reactions that may be severe or fatal, may occur after discontinuation of treatment, and may require corticosteroid treatment and interruption or discontinuation of KEYTRUDA QLEX. These reactions may include:
  - Pneumonitis: Advise patients to contact their healthcare provider immediately for new or worsening cough, chest pain, or shortness of breath [see Warnings and Precautions (5.1)].
  - Colitis: Advise patients to contact their healthcare provider immediately for diarrhea or severe abdominal pain [see Warnings and Precautions (5.1)].
  - Hepatitis: Advise patients to contact their healthcare provider immediately for jaundice, severe nausea or vomiting, or easy bruising or bleeding [see Warnings and Precautions (5.1)].
  - Endocrinopathies: Advise patients to contact their healthcare provider immediately for signs or symptoms of adrenal insufficiency, hypophysitis, hypothyroidism, hyperthyroidism, or Type 1 diabetes mellitus [see Warnings and Precautions (5.1)].
  - Nephritis: Advise patients to contact their healthcare provider immediately for signs or symptoms of nephritis [see Warnings and Precautions (5.1)].
  - Severe skin reactions: Advise patients to contact their healthcare provider immediately for any signs or symptoms of severe skin reactions, SJS or TEN [see Warnings and Precautions (5.1)].
  - Other immune-mediated adverse reactions:
    - Advise patients that immune-mediated adverse reactions can occur and may involve any organ system, and to contact their healthcare provider immediately for any new or worsening signs or symptoms [see Warnings and Precautions (5.1)].
    - Advise patients of the risk of solid organ transplant rejection and other transplant (including corneal graft) rejection. Advise patients to contact their healthcare provider immediately for signs or symptoms of organ transplant rejection and other transplant (including corneal graft) rejection [see Warnings and Precautions (5.1)].

Hypersensitivity and Administration-Related Reactions

- Advise patients to contact their healthcare provider immediately for signs or symptoms of hypersensitivity and administration-related systemic reactions [see Warnings and Precautions (5.2)].

Complications of Allogeneic HSCT

- Advise patients of the risk of post-allogeneic hematopoietic stem cell transplantation complications [see Warnings and Precautions (5.3)].

Embryo-Fetal Toxicity

- Advise females of reproductive potential of the potential risk to a fetus and to inform their healthcare provider of a known or suspected pregnancy [see Warnings and Precautions (5.5), Use in Specific Populations (8.1, 8.3)].
- Advise females of reproductive potential to use effective contraception during treatment with KEYTRUDA QLEX and for 4 months after the last dose [see Warnings and Precautions (5.5), Use in Specific Populations (8.1, 8.3)].

Lactation

- Advise women not to breastfeed during treatment with KEYTRUDA QLEX and for 4 months after the last dose [see Use in Specific Populations (8.2)].

Laboratory Tests

- Advise patients of the importance of keeping scheduled appointments for blood work or other laboratory tests [see Warnings and Precautions (5.1)].

Manufactured by: Merck Sharp & Dohme LLC
Rahway, NJ 07065, USA
U.S. License No. 0002

For patent information: www.msd.com/research/patent

The trademarks depicted herein are owned by their respective owners.

Copyright © 2026 Merck & Co., Inc., Rahway, NJ, USA, and its affiliates.
All rights reserved.

uspi-mk3475a-i-2602r003

MEDICATION GUIDE
KEYTRUDA QLEX™ (key-true-duh Q-lex)
(pembrolizumab and berahyaluronidase alfa-pmph)
injection, for subcutaneous use

What is the most important information I should know about KEYTRUDA QLEX?

KEYTRUDA QLEX is a medicine that may treat certain cancers by working with your immune system. KEYTRUDA QLEX can cause your immune system to attack normal organs and tissues in any area of your body and can affect the way they work. These problems can sometimes become severe or life-threatening and can lead to death. You can have more than one of these problems at the same time. These problems may happen anytime during treatment or even after your treatment has ended.

Call or see your healthcare provider right away if you develop any new or worsening signs or symptoms, including:

Lung problems

- cough

- shortness of breath

- chest pain

Intestinal problems

- diarrhea (loose stools) or more frequent bowel movements than usual
- stools that are black, tarry, sticky, or have blood or mucus
- severe stomach-area (abdomen) pain or tenderness

Liver problems

- yellowing of your skin or the whites of your eyes
- severe nausea or vomiting
- pain on the right side of your stomach area (abdomen)

- dark urine (tea colored)
- bleeding or bruising more easily than normal

Hormone gland problems

- headaches that will not go away or unusual headaches
- eye sensitivity to light
- eye problems
- rapid heartbeat
- increased sweating
- extreme tiredness
- weight gain or weight loss
- feeling more hungry or thirsty than usual

- urinating more often than usual
- hair loss
- feeling cold
- constipation
- your voice gets deeper
- dizziness or fainting
- changes in mood or behavior, such as decreased sex drive, irritability, or forgetfulness

Kidney problems

- decrease in your amount of urine
- blood in your urine

- swelling of your ankles
- loss of appetite

Skin problems

- rash
- itching
- skin blistering or peeling

- painful sores or ulcers in your mouth or in your nose, throat, or genital area
- fever or flu-like symptoms
- swollen lymph nodes

Problems can also happen in other organs and tissues. These are not all of the signs and symptoms of immune system problems that can happen with KEYTRUDA QLEX. Call or see your healthcare provider right away for any new or worsening signs or symptoms, which may include:

- chest pain, irregular heartbeat, shortness of breath, swelling of ankles
- confusion, sleepiness, memory problems, changes in mood or behavior, stiff neck, balance problems, tingling or numbness of the arms or legs
- double vision, blurry vision, sensitivity to light, eye pain, changes in eyesight
- persistent or severe muscle pain or weakness, muscle cramps
- low red blood cells, bruising

Allergic and injection-related reactions that can sometimes be severe or life-threatening, can happen during treatment with KEYTRUDA QLEX. Tell your healthcare provider right away if you get any signs or symptoms, including:

- chills or shaking
- itching or rash
- flushing
- shortness of breath or wheezing

- dizziness
- feeling like passing out
- fever
- back pain

Rejection of a transplanted organ or tissue. Your healthcare provider should tell you what signs and symptoms you should report and monitor you depending on the type of organ or tissue transplant that you have had.

Complications, including graft-versus-host-disease (GVHD), in people who have received a bone marrow (stem cell) transplant that uses donor stem cells (allogeneic). These complications can be serious and can lead to death. These complications may happen if you underwent transplantation either before or after being treated with KEYTRUDA QLEX. Your healthcare provider will monitor you for these complications.

Getting medical treatment right away may help keep these problems from becoming more serious.

Your healthcare provider will check you for these problems during treatment with KEYTRUDA QLEX. Your healthcare provider may treat you with corticosteroid or hormone replacement medicines. Your healthcare provider may also need to delay or completely stop treatment with KEYTRUDA QLEX if you have severe side effects.

What is KEYTRUDA QLEX?

KEYTRUDA QLEX is a prescription medicine used to treat:

- a kind of skin cancer called melanoma. KEYTRUDA QLEX may be used:
  - when your melanoma has spread or cannot be removed by surgery (advanced melanoma), or
  - in adults and children 12 years of age and older with Stage IIB, Stage IIC, or Stage III melanoma, to help prevent melanoma from coming back after it and lymph nodes that contain cancer have been removed by surgery.
- a kind of lung cancer called non-small cell lung cancer (NSCLC).
  - KEYTRUDA QLEX may be used with the chemotherapy medicines pemetrexed and a platinum as your first treatment when your lung cancer:
    - has spread (advanced NSCLC), and
    - is a type called “nonsquamous”, and
    - your tumor does not have an abnormal “EGFR” or “ALK” gene.
  - KEYTRUDA QLEX may be used with the chemotherapy medicines carboplatin and either paclitaxel or paclitaxel protein-bound as your first treatment when your lung cancer:
    - has spread (advanced NSCLC), and
    - is a type called “squamous”.
  - KEYTRUDA QLEX may be used alone as your first treatment when your lung cancer:
    - has not spread outside your chest (Stage III) and you cannot have surgery or chemotherapy with radiation or
    - your NSCLC has spread to other areas of your body (advanced NSCLC), and
    - your tumor tests positive for “PD-L1”, and
    - does not have an abnormal “EGFR” or “ALK” gene.
  - KEYTRUDA QLEX may also be used alone when:
    - you have received chemotherapy that contains platinum to treat your advanced NSCLC, and it did not work or it is no longer working, and
    - your tumor tests positive for “PD-L1”, and
    - if your tumor has an abnormal “EGFR” or “ALK” gene, you have also received an EGFR or ALK inhibitor medicine and it did not work or is no longer working.
  - KEYTRUDA QLEX may be used in combination with chemotherapy that contains platinum and another chemotherapy medicine:
    - before surgery when you have early-stage NSCLC which can be removed by surgery, and
    - then continued alone after surgery to help prevent your lung cancer from coming back.
  - KEYTRUDA QLEX may be used alone as a treatment in adults for your lung cancer:
    - to help prevent your lung cancer from coming back after your tumor(s) has been removed by surgery and you have received platinum-based chemotherapy, and
    - you have Stage IB and your tumor(s) is 4 cm or greater in size, Stage II, or Stage IIIA NSCLC.
- a kind of cancer in adults called malignant pleural mesothelioma (MPM) that affects the lining of the lungs and chest wall.
  - KEYTRUDA QLEX may be used in combination with the chemotherapy medicines pemetrexed and a platinum as your first treatment when your cancer has spread or cannot be removed by surgery (advanced MPM).
- a kind of cancer called head and neck squamous cell cancer (HNSCC).
  - KEYTRUDA QLEX may be used alone in adults with HNSCC before surgery:
    - when your cancer can be removed by surgery, has spread to nearby tissues, and your tumor tests positive for “PD-L1”, and
    - then continued in combination with radiation with or without cisplatin after surgery, and
    - then continued alone to help prevent your head and neck cancer from coming back.
  - KEYTRUDA QLEX may be used with the chemotherapy medicines fluorouracil and a platinum as your first treatment when your head and neck cancer has spread or returned and cannot be removed by surgery.
  - KEYTRUDA QLEX may be used alone as your first treatment when your head and neck cancer:
    - has spread or returned and cannot be removed by surgery, and
    - your tumor tests positive for “PD-L1”.
  - KEYTRUDA QLEX may be used alone when your head and neck cancer:
    - has spread or returned, and
    - you have received chemotherapy that contains platinum and it did not work or is no longer working.
- a kind of bladder and urinary tract cancer called urothelial cancer.
  - KEYTRUDA QLEX may be used with the medicine enfortumab vedotin in adults when your bladder or urinary tract cancer has spread or cannot be removed by surgery (locally advanced or metastatic urothelial cancer).
  - KEYTRUDA QLEX may be used alone when your bladder or urinary tract cancer:
    - has spread or cannot be removed by surgery (locally advanced or metastatic urothelial cancer), and
    - you are not able to receive chemotherapy that contains platinum (medicines called either cisplatin or carboplatin), or
    - you have received chemotherapy that contains platinum, and it did not work or is no longer working.
  - KEYTRUDA QLEX may be used with the medicine enfortumab vedotin in adults before and after the surgical removal of your bladder when:
    - your bladder cancer has spread into the muscle layer of the bladder (muscle invasive bladder cancer [MIBC]) but not to other parts of the body, and
    - you are not able to receive chemotherapy that contains cisplatin.
  - KEYTRUDA QLEX may be used alone when your cancer has not spread to nearby tissue in the bladder, but is at high-risk for spreading (high-risk non-muscle-invasive bladder cancer [NMIBC]) when:
    - your tumor is a type called “carcinoma in situ” (CIS), and
    - you have tried treatment with Bacillus Calmette-Guerin (BCG) and it did not work, and
    - you are not able to or have decided not to have surgery to remove your bladder.
- a kind of cancer that is shown by a laboratory test to be a microsatellite instability-high (MSI-H) or a mismatch repair deficient (dMMR) solid tumor. KEYTRUDA QLEX may be used in adults and children 12 years of age and older to treat:
  - cancer that has spread or cannot be removed by surgery (advanced cancer), and
  - has progressed following treatment, and you have no satisfactory treatment options.
- a kind of cancer called colon or rectal cancer. KEYTRUDA QLEX may be used when your cancer:
  - has spread or cannot be removed by surgery (advanced colon or rectal cancer), and
  - has been shown by a laboratory test to be microsatellite instability-high (MSI-H) or mismatch repair deficient (dMMR).
- a kind of stomach cancer called gastric or gastroesophageal junction (GEJ) adenocarcinoma.
  - KEYTRUDA QLEX may be used in adults in combination with the medicine trastuzumab along with fluoropyrimidine and platinum chemotherapy as your first treatment when your stomach cancer:
    - is HER2-positive, and your tumor tests positive for “PD-L1”, and
    - has spread or cannot be removed by surgery (advanced gastric cancer).
  - KEYTRUDA QLEX may be used in adults in combination with fluoropyrimidine and platinum chemotherapy as your first treatment when your stomach cancer:
    - is HER2-negative, and your tumor tests positive for “PD-L1”, and
    - has spread or cannot be removed by surgery (advanced gastric cancer).
- a kind of cancer called esophageal or certain gastroesophageal junction (GEJ) carcinomas that cannot be cured by surgery or a combination of chemotherapy and radiation therapy.
  - KEYTRUDA QLEX may be used in combination with platinum- and fluoropyrimidine-based chemotherapy medicines when your tumor tests positive for “PD-L1”.
  - KEYTRUDA QLEX may be used alone when:
    - you have received one or more types of treatment, and it did not work or it is no longer working, and
    - your tumor is a type called “squamous”, and
    - your tumor tests positive for “PD-L1”.
- a kind of cancer called cervical cancer.
  - KEYTRUDA QLEX may be used with chemotherapy and radiation therapy when your cervical cancer has spread nearby to the lower part of your vagina or to pelvic organs or has affected your kidneys (Stage III to IVA FIGO 2014 classification).
  - KEYTRUDA QLEX may be used with chemotherapy medicines, with or without the medicine bevacizumab, when:
    - your cervical cancer does not go away (persistent), has returned, or has spread (advanced cervical cancer), and
    - your tumor tests positive for “PD-L1”.
  - KEYTRUDA QLEX may be used alone when your cervical cancer:
    - has returned, or has spread (advanced cervical cancer), and
    - you have received chemotherapy, and it did not work or is no longer working, and
    - your tumor tests positive for “PD-L1”.
- a kind of liver cancer called hepatocellular carcinoma (HCC). KEYTRUDA QLEX may be used when:
  - you have HCC after having hepatitis B, and
  - you have received anti-cancer treatment that did not contain a “PD-1” or “PD-L1” blocking medicine.
- a kind of bile duct or gallbladder cancer called biliary tract cancer (BTC). KEYTRUDA QLEX may be used with chemotherapy medicines gemcitabine and cisplatin when your biliary tract cancer has spread or cannot be removed by surgery.
- a kind of skin cancer called Merkel cell carcinoma (MCC) in adults and children 12 years of age and older. KEYTRUDA QLEX may be used to treat your skin cancer when it has spread or returned.
- a kind of kidney cancer called renal cell carcinoma (RCC).
  - KEYTRUDA QLEX may be used in adults with the medicine axitinib as your first treatment when your kidney cancer has spread or cannot be removed by surgery (advanced RCC).
  - KEYTRUDA QLEX may be used in adults with the medicine lenvatinib as your first treatment when your kidney cancer has spread or cannot be removed by surgery (advanced RCC).
  - KEYTRUDA QLEX may be used alone if you are at intermediate-high or high risk of your kidney cancer (RCC) coming back after surgery to:
    - remove all or part of your kidney, or
    - remove all or part of your kidney and also surgery to remove cancer that has spread to other parts of the body (metastatic lesions).
- a kind of uterine cancer called advanced endometrial carcinoma.
  - KEYTRUDA QLEX may be used with the chemotherapy medicines carboplatin and paclitaxel, and then KEYTRUDA QLEX may be used alone, in adults:
    - when your cancer has spread (advanced), or
    - if your cancer has returned.
  - KEYTRUDA QLEX may be used with the medicine lenvatinib in adults:
    - when a laboratory test shows that your tumor is mismatch repair proficient (pMMR) or not microsatellite instability-high (MSI-H), and
    - you have received anti-cancer treatment, and it is no longer working, and
    - your cancer cannot be cured by surgery or radiation.
  - KEYTRUDA QLEX may be used alone in adults:
    - if your cancer is shown by a laboratory test to be microsatellite instability-high (MSI-H) or mismatch repair deficient (dMMR), and
    - you have received anti-cancer treatment and it is no longer working, and
    - your cancer cannot be cured by surgery or radiation.
- a kind of cancer that is shown by a test to be tumor mutational burden-high (TMB-H). KEYTRUDA QLEX may be used in adults and children 12 years of age and older to treat:
  - solid tumors that have spread or cannot be removed by surgery (advanced cancer), and
  - you have received anti-cancer treatment, and it did not work or is no longer working, and
  - you have no satisfactory treatment options.
  It is not known if KEYTRUDA QLEX is safe and effective in children 12 years of age and older with TMB-H cancers of the brain or spinal cord (central nervous system cancers).
- a kind of skin cancer called cutaneous squamous cell carcinoma (cSCC). KEYTRUDA QLEX may be used when your skin cancer:
  - has returned or spread, and
  - cannot be cured by surgery or radiation.
- a kind of cancer called triple-negative breast cancer (TNBC).
  - KEYTRUDA QLEX may be used with chemotherapy medicines as treatment before surgery and then continued alone after surgery when you:
    - have early-stage breast cancer, and
    - are at high risk of your breast cancer coming back.
  - KEYTRUDA QLEX may be used with chemotherapy medicines when your breast cancer:
    - has returned and cannot be removed by surgery or has spread, and
    - tests positive for “PD-L1”.
- a kind of cancer called ovarian cancer.
  - KEYTRUDA QLEX may be used in adults with the chemotherapy medicine paclitaxel, with or without the medicine bevacizumab, when your ovarian, fallopian tube, or primary peritoneal cancer:
    - is resistant to chemotherapy that contains platinum, and
    - tests positive for “PD-L1”, and
    - you have received 1or 2 types of treatment.

It is not known if KEYTRUDA QLEX is safe and effective in children younger than 12 years of age with melanoma, MCC, MSI-H or dMMR cancer, or TMB-H cancer. It is not known if KEYTRUDA QLEX is safe and effective in children for the treatment of any other cancers that KEYTRUDA QLEX is used to treat.

Who should not receive KEYTRUDA QLEX?
Do not receive KEYTRUDA QLEX if you are allergic to berahyaluronidase, hyaluronidase or any of the inactive ingredients in KEYTRUDA QLEX. See the end of this Medication Guide for a complete list of ingredients in KEYTRUDA QLEX.

Before receiving KEYTRUDA QLEX, tell your healthcare provider about all of your medical conditions, including if you:

- have immune system problems such as Crohn’s disease, ulcerative colitis, or lupus
- have received an organ or tissue transplant, including corneal transplant
- have received or plan to receive a stem cell transplant that uses donor stem cells (allogeneic)
- have received radiation treatment to your chest area
- have a condition that affects your nervous system, such as myasthenia gravis or Guillain-Barré syndrome
- are pregnant or plan to become pregnant. KEYTRUDA QLEX can harm your unborn baby.
  Females who are able to become pregnant:
  - Your healthcare provider will give you a pregnancy test before you start treatment with KEYTRUDA QLEX.
  - You should use an effective method of birth control during treatment with KEYTRUDA QLEX and for 4 months after the last dose of KEYTRUDA QLEX. Talk to your healthcare provider about birth control methods that you can use during this time.
  - Tell your healthcare provider right away if you think you may be pregnant or if you become pregnant during treatment with KEYTRUDA QLEX.
- are breastfeeding or plan to breastfeed. It is not known if KEYTRUDA QLEX passes into your breast milk. Do not breastfeed during treatment with KEYTRUDA QLEX and for 4 months after your last dose of KEYTRUDA QLEX.

Tell your healthcare provider about all the medicines you take, including prescription and over-the-counter medicines, vitamins, and herbal supplements.

How will I receive KEYTRUDA QLEX?

- Your healthcare provider will give you KEYTRUDA QLEX as an injection under the skin (subcutaneous) in the stomach area (abdomen) or thigh.
- KEYTRUDA QLEX is usually given every 3 weeks over 1 minute or every 6 weeks over 2 minutes depending on the dose of KEYTRUDA QLEX that you are receiving.
- Your healthcare provider will decide how many treatments you need.
- Your healthcare provider will do blood tests to check you for side effects.
- If you miss any appointments, call your healthcare provider as soon as possible to reschedule your appointment.

What are the possible side effects of KEYTRUDA QLEX?

KEYTRUDA QLEX can cause serious side effects. See “What is the most important information I should know about KEYTRUDA QLEX?”

The most common side effects of KEYTRUDA QLEX when given with certain chemotherapy medicines include: nausea, tiredness, and muscle, bone, and joint pain.

The most common side effects seen with pembrolizumab given into the vein (intravenous pembrolizumab), which may happen with KEYTRUDA QLEX, are shown below:

- when used alone include: feeling tired, pain, including pain in muscles, rash, diarrhea, fever, cough, decreased appetite, itching, shortness of breath, constipation, bones or joints and stomach-area (abdominal) pain, nausea, and low levels of thyroid hormone.
- when used alone that are more common in children than in adults include: fever, vomiting, headache, stomach area (abdominal) pain, and low levels of white blood cells.
- when used with certain chemotherapy or chemotherapy with radiation therapy medicines include: feeling tired or weak, nausea, constipation, diarrhea, decreased appetite, rash, vomiting, cough, trouble breathing, fever, hair loss, inflammation of the nerves that may cause pain, weakness, and paralysis in the arms and legs, swelling of the lining of the mouth, nose, eyes, throat, intestines, or vagina, mouth sores, headache, weight loss, stomach-area (abdominal) pain, joint and muscle pain, trouble sleeping, blisters or rash on the palms of your hands and soles of your feet, urinary tract infection, low levels of thyroid hormone, skin irritation in the radiation area, trouble swallowing, and dry mouth.
- when used with chemotherapy and bevacizumab include: tingling or numbness of the arms or legs, hair loss, low red blood cell count, feeling tired or weak, nausea, low white blood cell count, diarrhea, high blood pressure, decreased platelet count, constipation, joint aches, vomiting, urinary tract infection, rash, low levels of thyroid hormone, decreased appetite, fever, mouth sores, and nosebleed.
- when used with axitinib include: diarrhea, feeling tired or weak, high blood pressure, liver problems, low levels of thyroid hormone, decreased appetite, blisters or rash on the palms of your hands and soles of your feet, nausea, mouth sores or swelling of the lining of the mouth, nose, eyes, throat, intestines, or vagina, hoarseness, rash, cough, and constipation.
- when used with lenvatinib include: low levels of thyroid hormone, high blood pressure, feeling tired, diarrhea, joint and muscle pain, nausea, decreased appetite, vomiting, mouth sores, weight loss, stomach-area (abdominal) pain, urinary tract infection, protein in your urine, constipation, headache, bleeding, blisters or rash on the palms of your hands and soles of your feet, hoarseness, rash, liver problems, and kidney problems.
- when used with enfortumab vedotin include: rash, tingling or numbness of the arms or legs, feeling tired, itching, diarrhea, hair loss, weight loss, decreased appetite, dry eye, nausea, constipation, changes in sense of taste, and urinary tract infection.

These are not all of the possible side effects of KEYTRUDA QLEX.
Call your doctor for medical advice about side effects. You may report side effects to FDA at 1-800-FDA-1088.

General information about the safe and effective use of KEYTRUDA QLEX

Medicines are sometimes prescribed for purposes other than those listed in a Medication Guide. You can ask your pharmacist or healthcare provider for information about KEYTRUDA QLEX that is written for health professionals.

What are the ingredients in KEYTRUDA QLEX?

Active ingredients: pembrolizumab and berahyaluronidase alfa-pmph

Inactive ingredients: histidine, histidine hydrochloride monohydrate, methionine, polysorbate 80, sucrose, and Water for Injection.

Manufactured by: Merck Sharp & Dohme LLC
Rahway, NJ 07065, USA
U.S. License No. 0002

For patent information: www.msd.com/research/patent
Copyright © 2026 Merck & Co., Inc., Rahway, NJ, USA, and its affiliates.
All rights reserved.
usmg-mk3475a-i-2602r003
For more information, go to www.keytruda.com/qlex.

This Medication Guide has been approved by the U.S. Food and Drug Administration.

Issued: 02/2026

PRINCIPAL DISPLAY PANEL - 395 mg and 4,800 units/2.4 mL Vial Carton

NDC 0006-3083-01

Keytruda Qlex ™

(pembrolizumab and
berahyaluronidase alfa-pmph) Injection

395 mg and 4,800 units/2.4 mL
(165 mg and 2,000 units/mL)

For Subcutaneous Use Only

Administer subcutaneous injection
over 1 minute

Dispense the enclosed Medication Guide to each patient.

One Single-dose vial. Discard unused portion.

Rx only

PRINCIPAL DISPLAY PANEL - 790 mg and 9,600 units/4.8 mL Vial Carton

NDC 0006-5083-01

Keytruda Qlex ™

(pembrolizumab and
berahyaluronidase alfa-pmph) Injection

790 mg and 9,600 units/4.8 mL
(165 mg and 2,000 units/mL)

For Subcutaneous Use Only

Administer subcutaneous injection
over 2 minutes

Dispense the enclosed Medication Guide to each patient.

One Single-dose vial. Discard unused portion.

Rx only